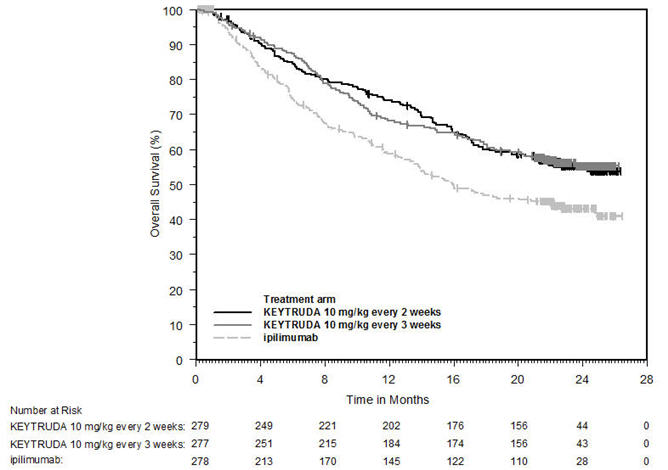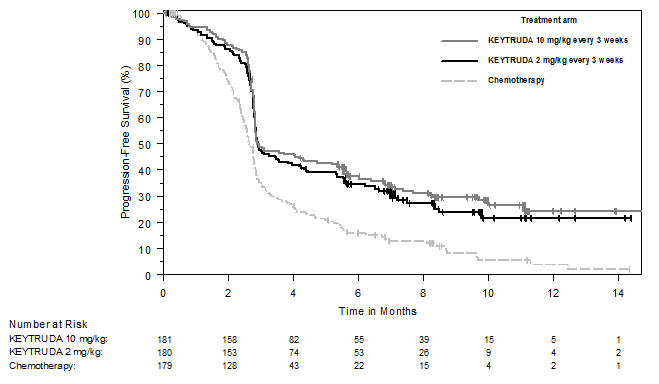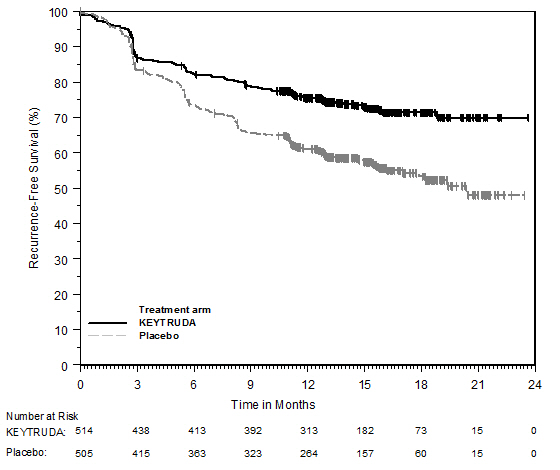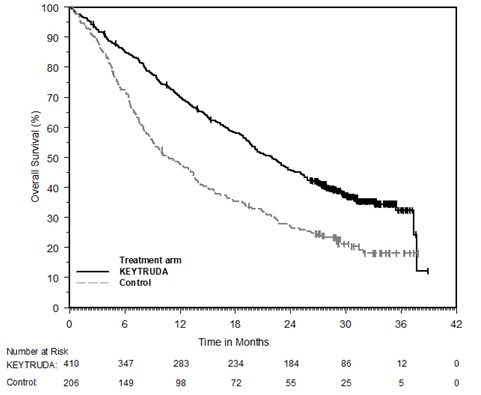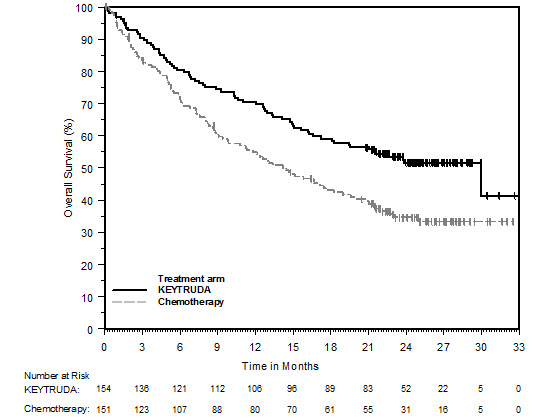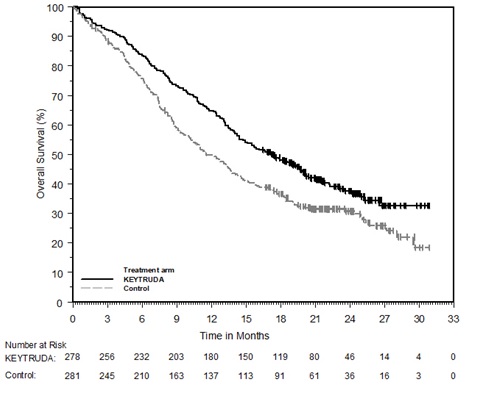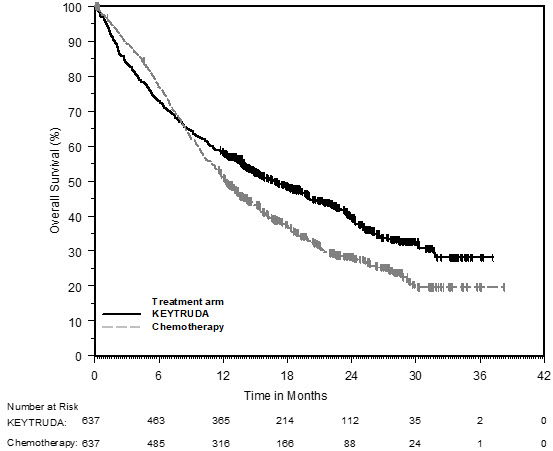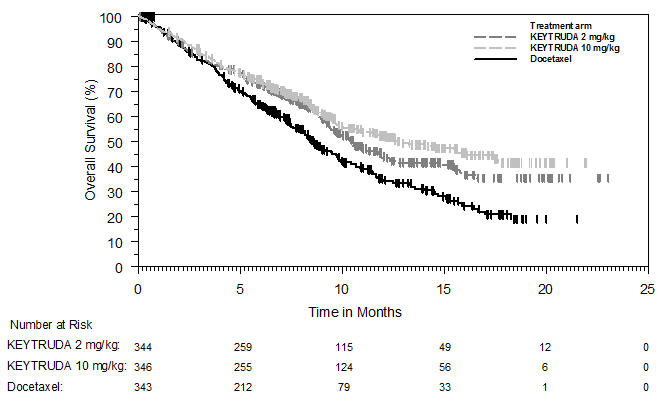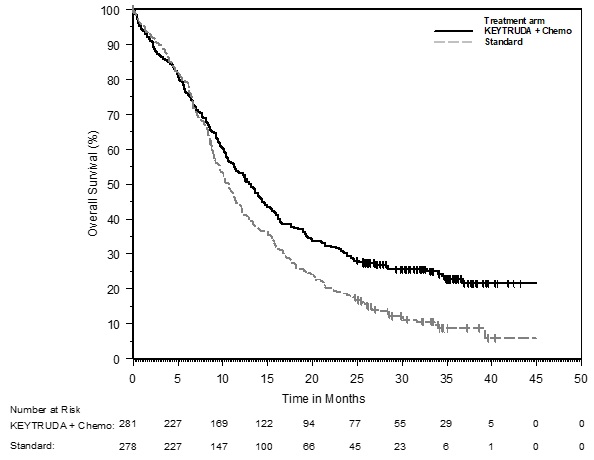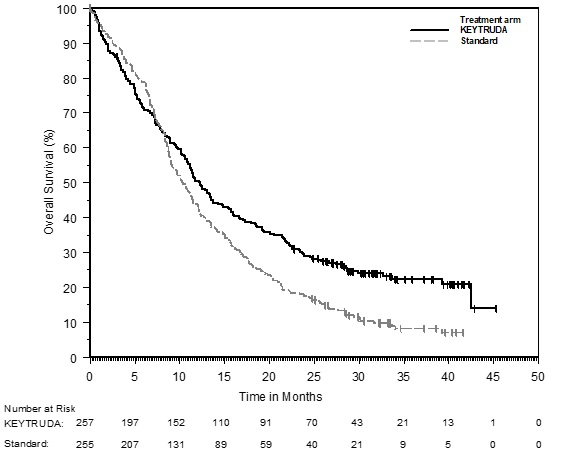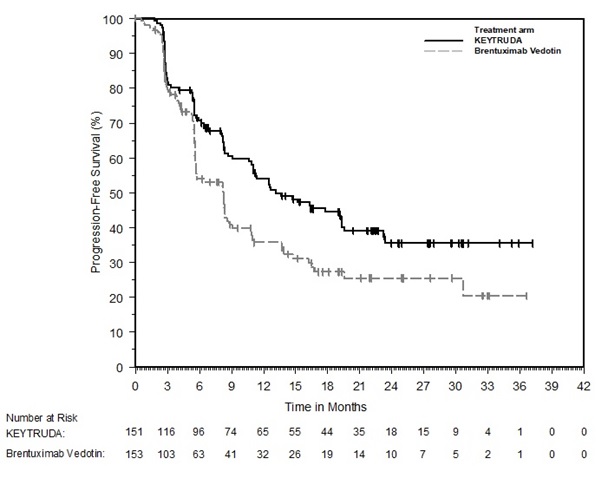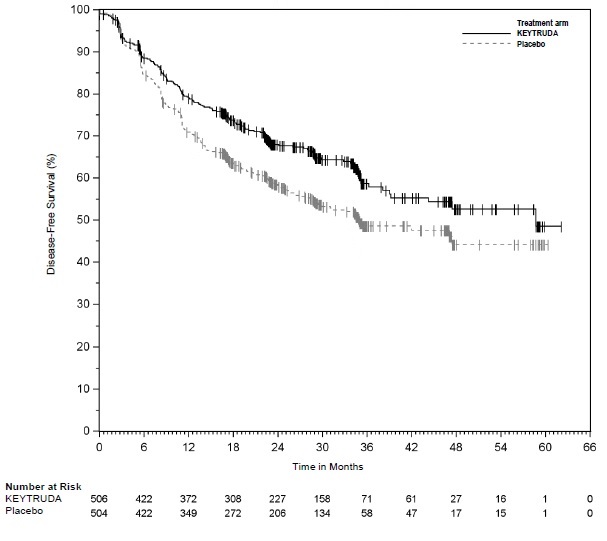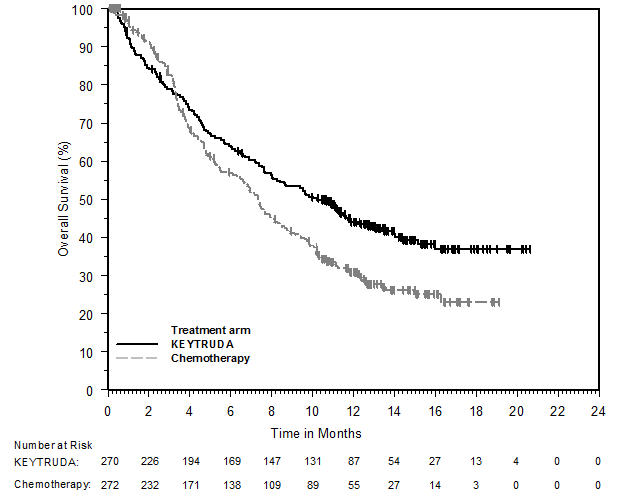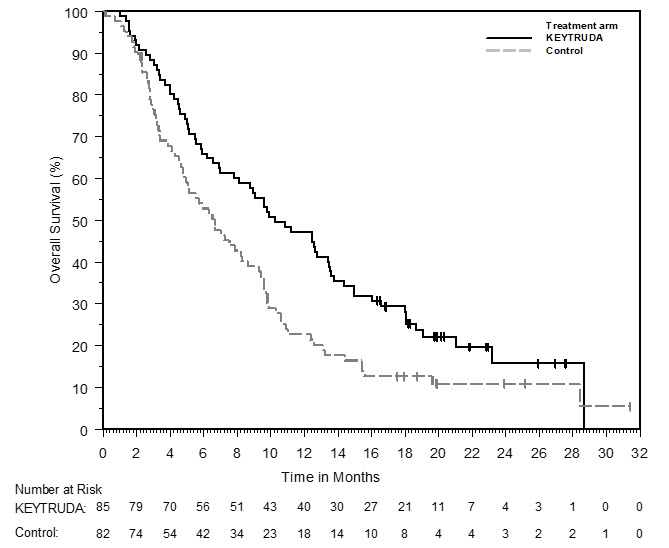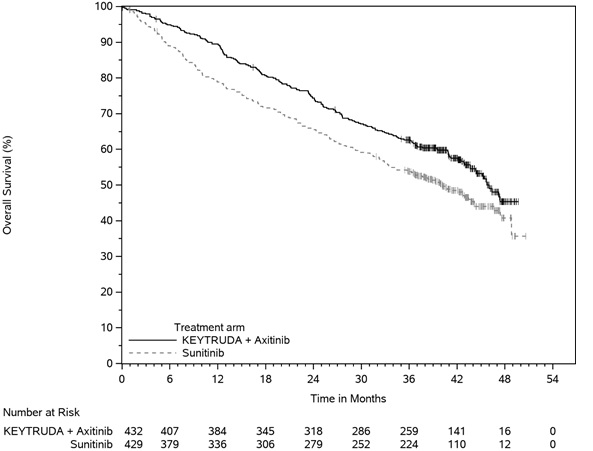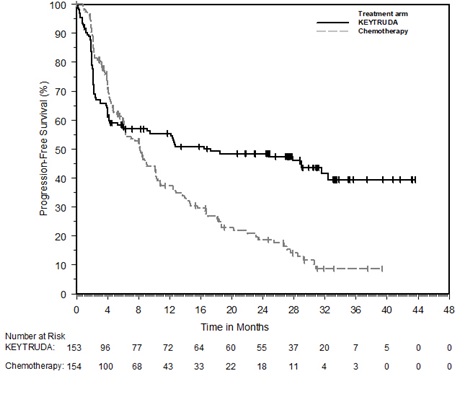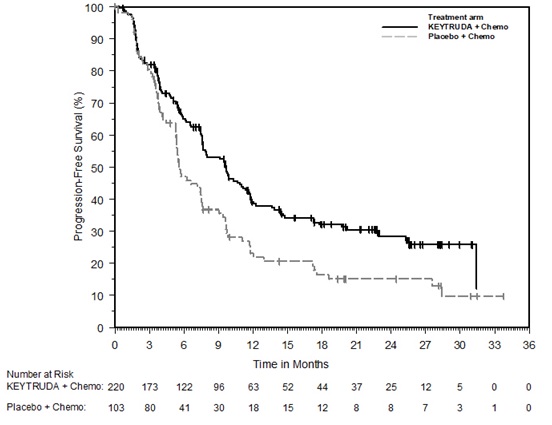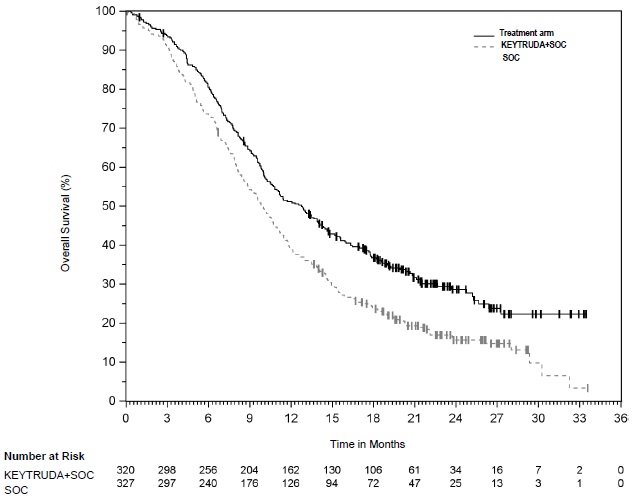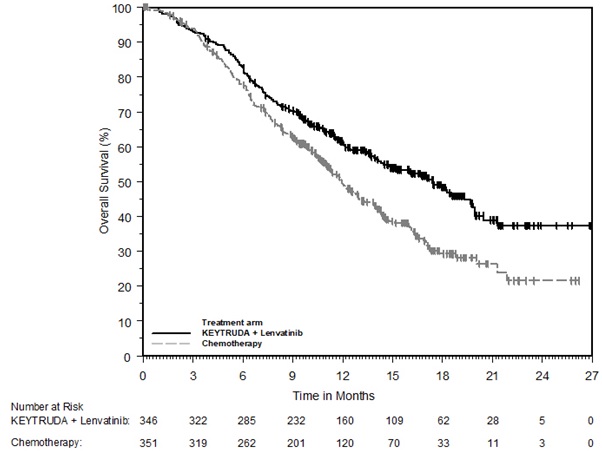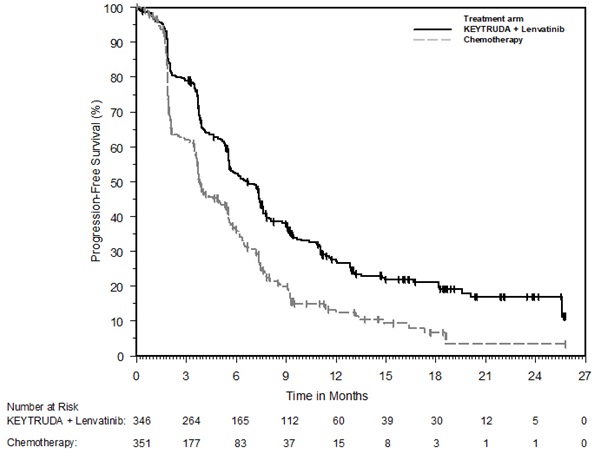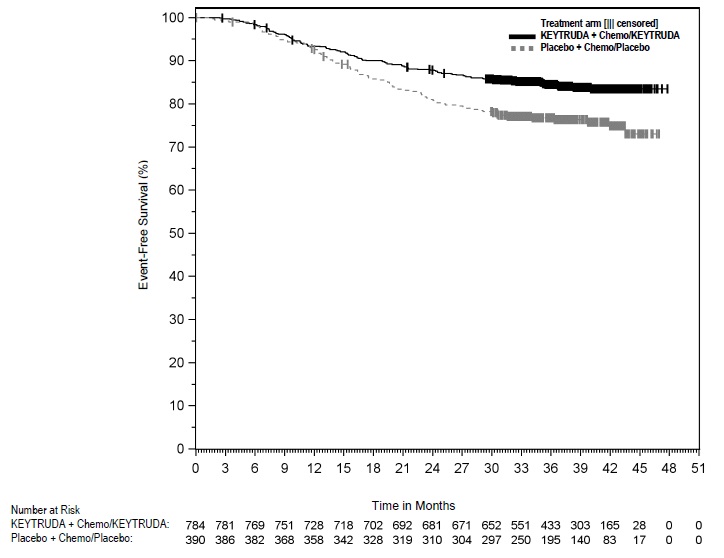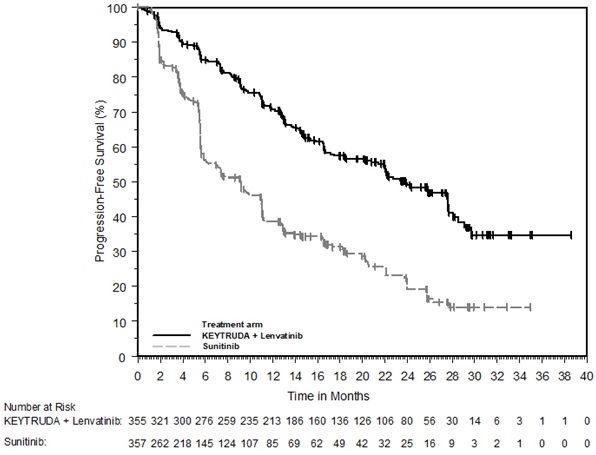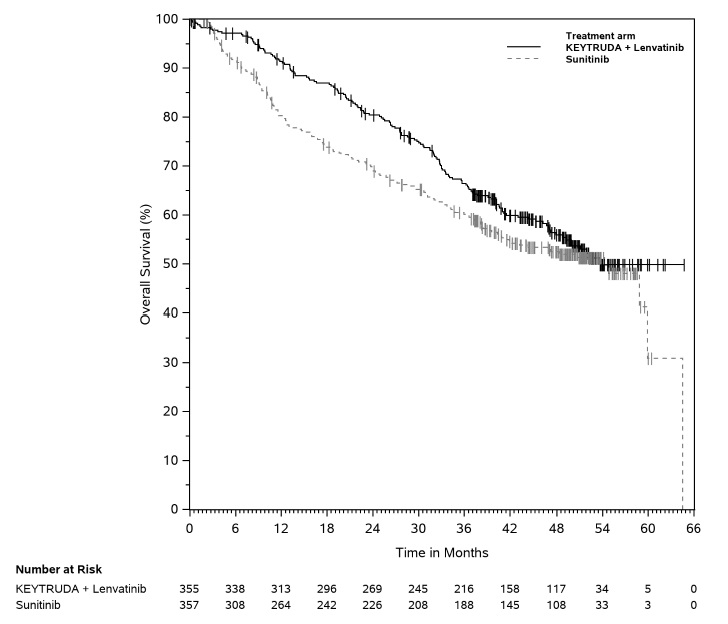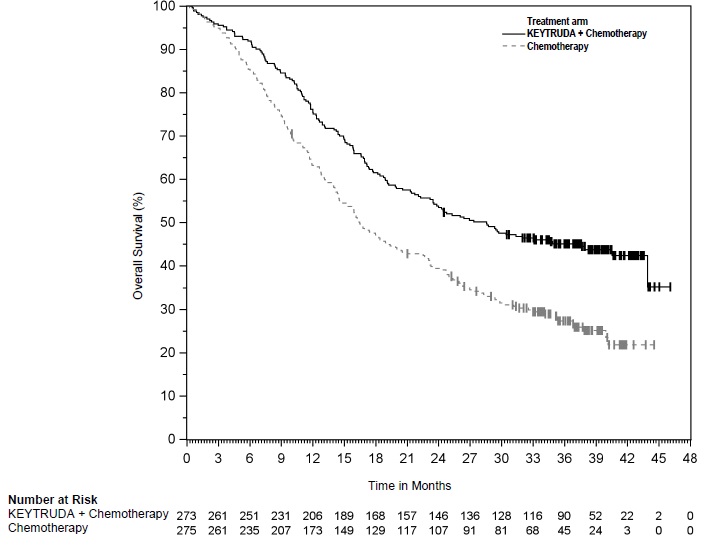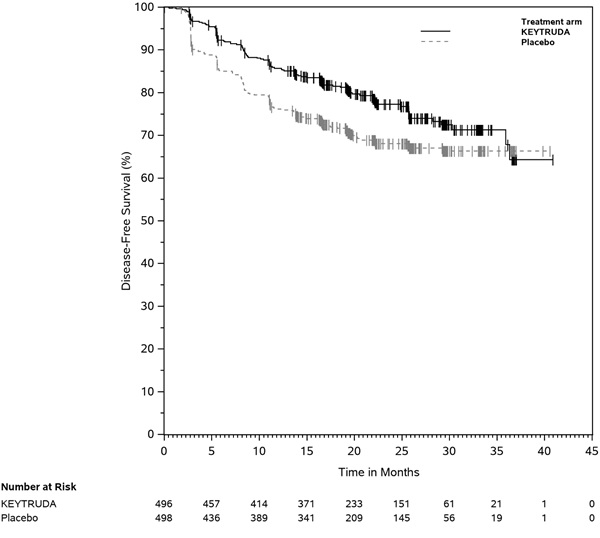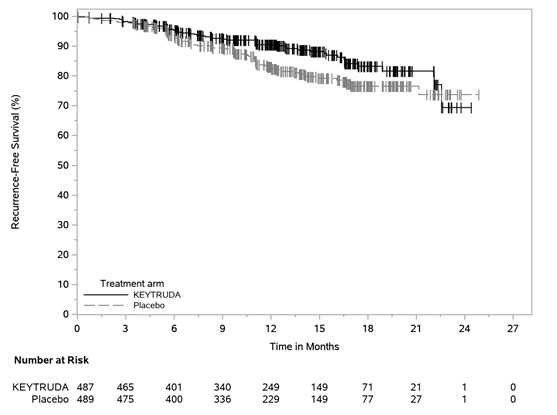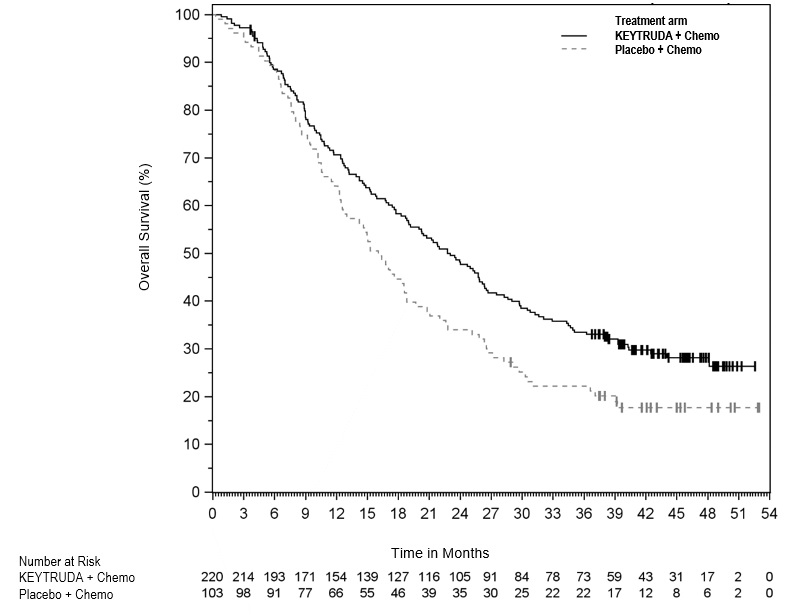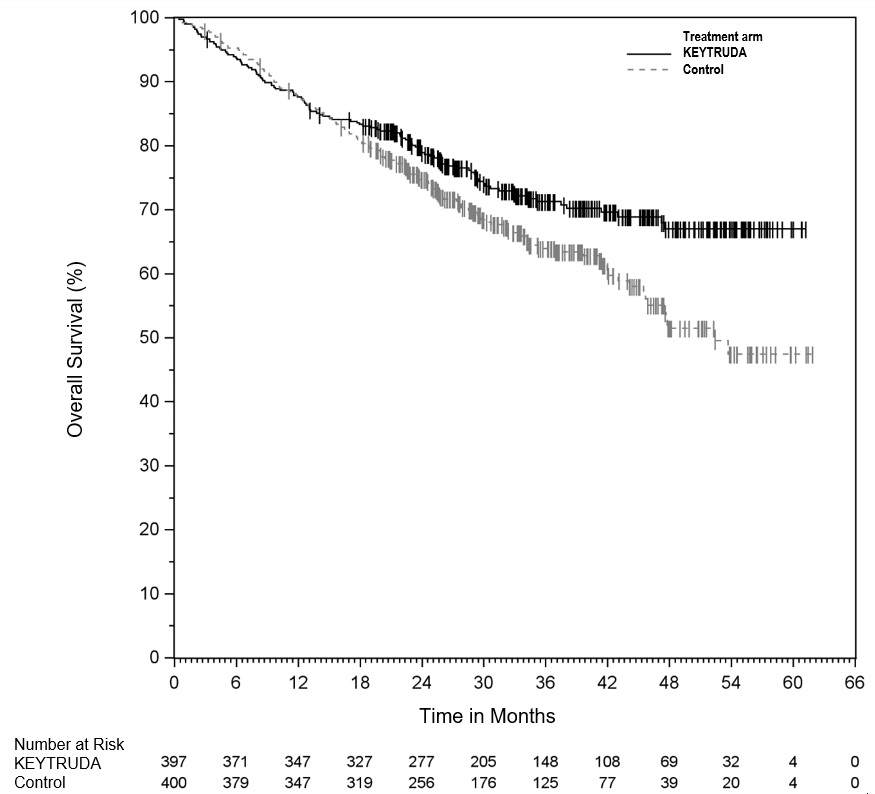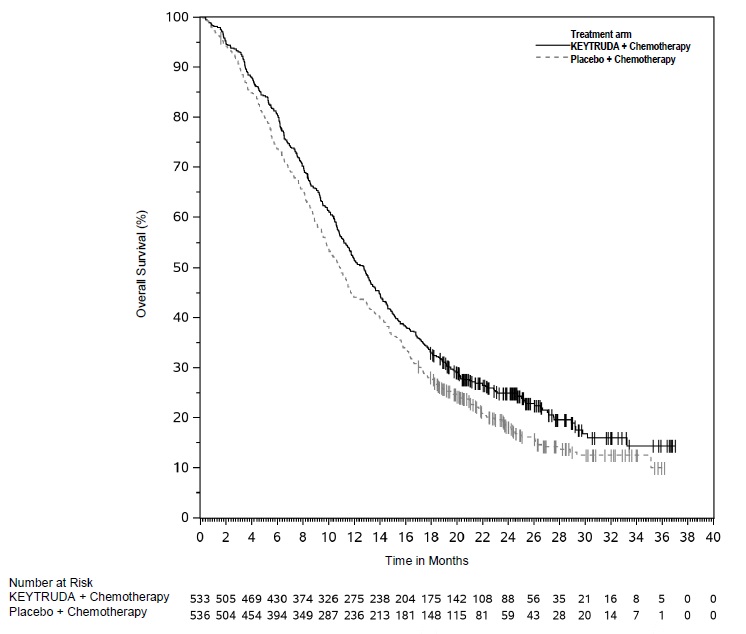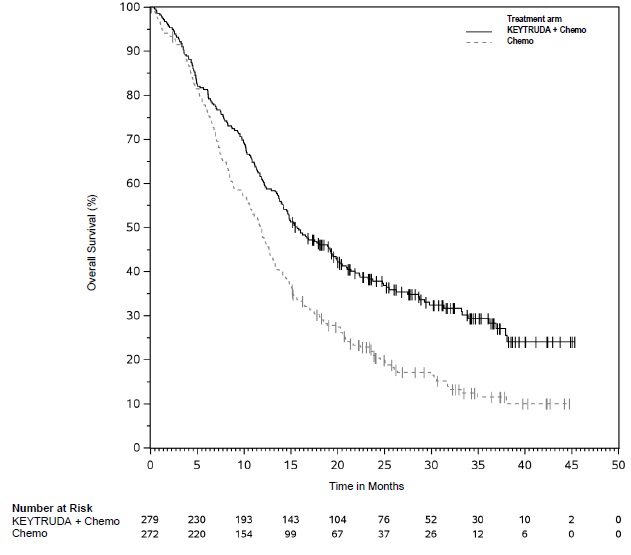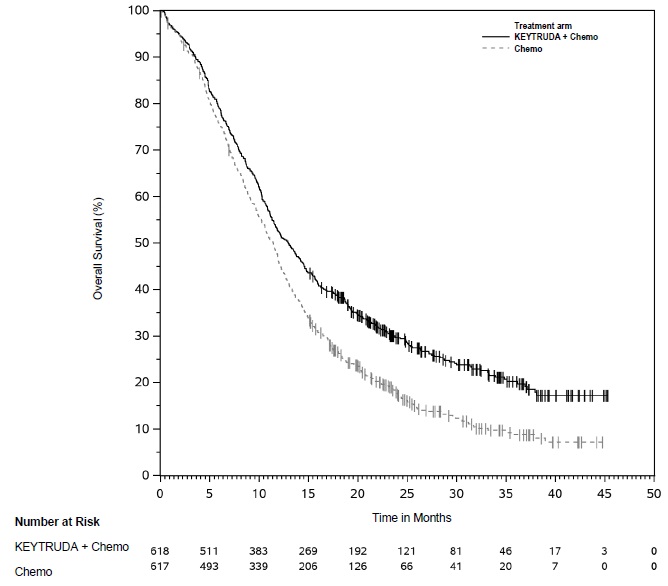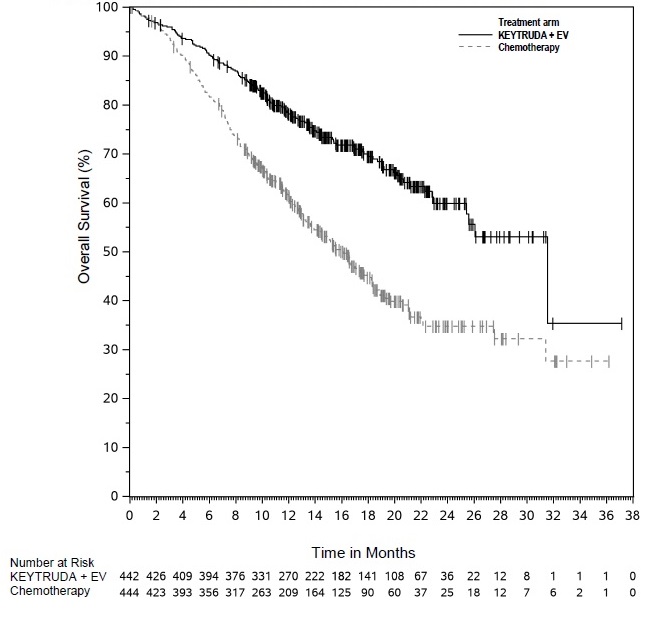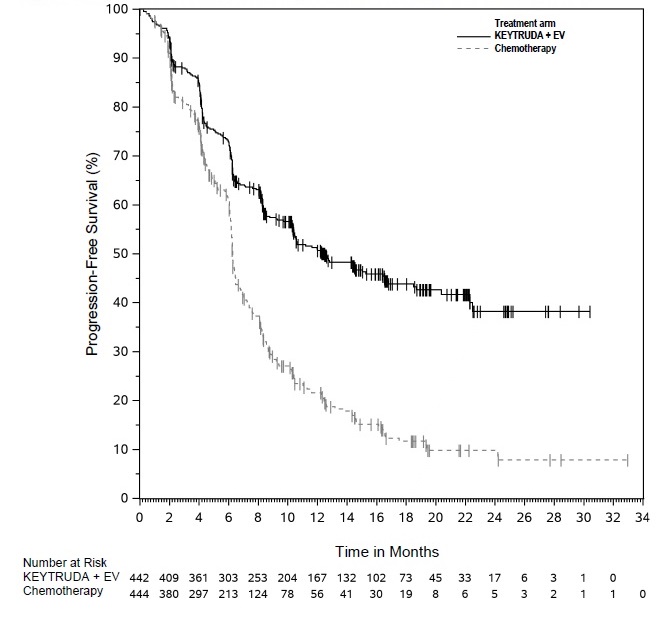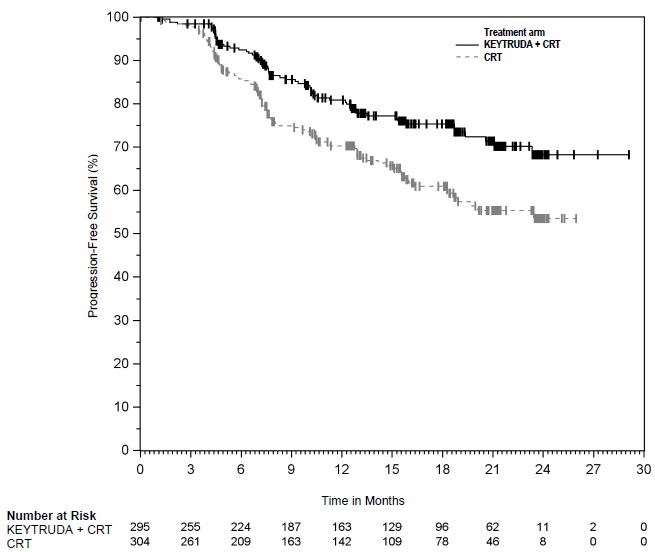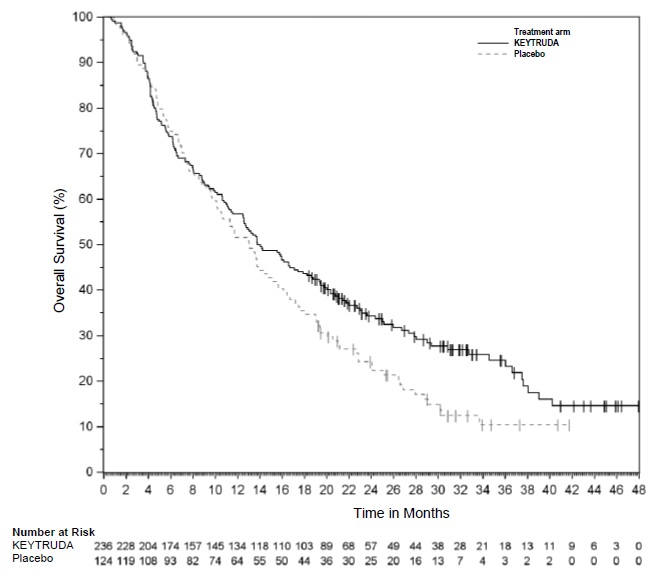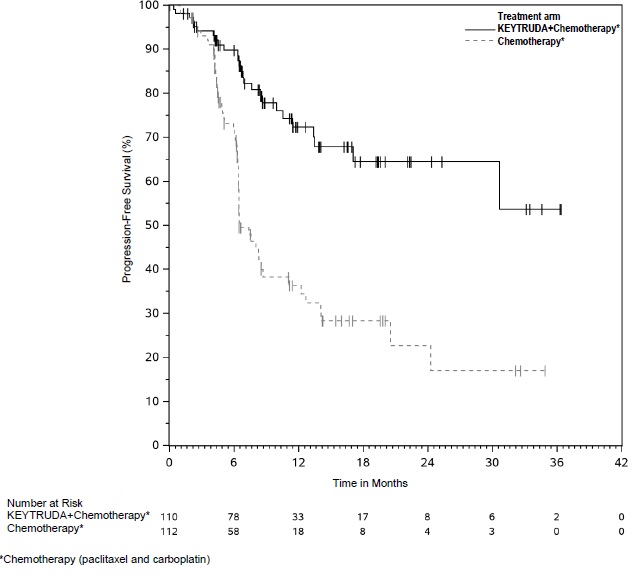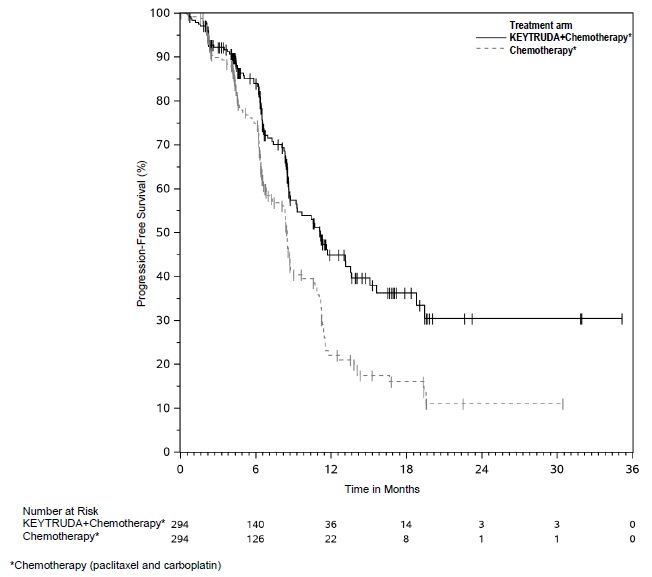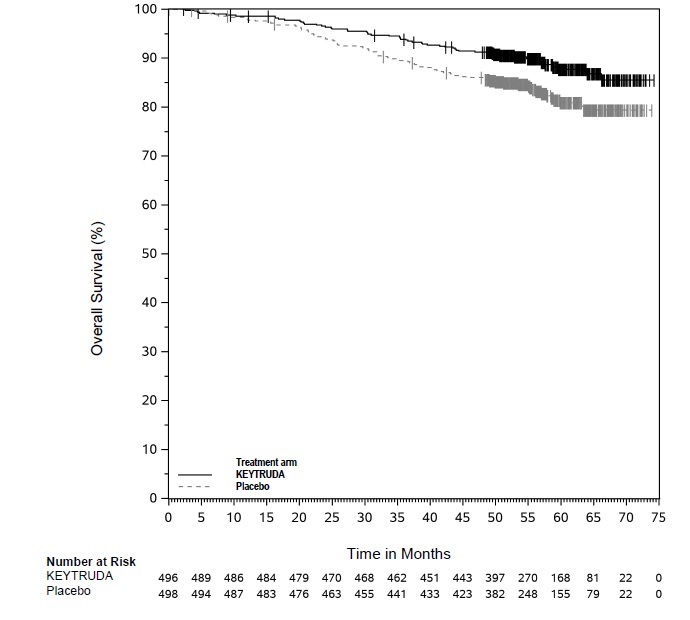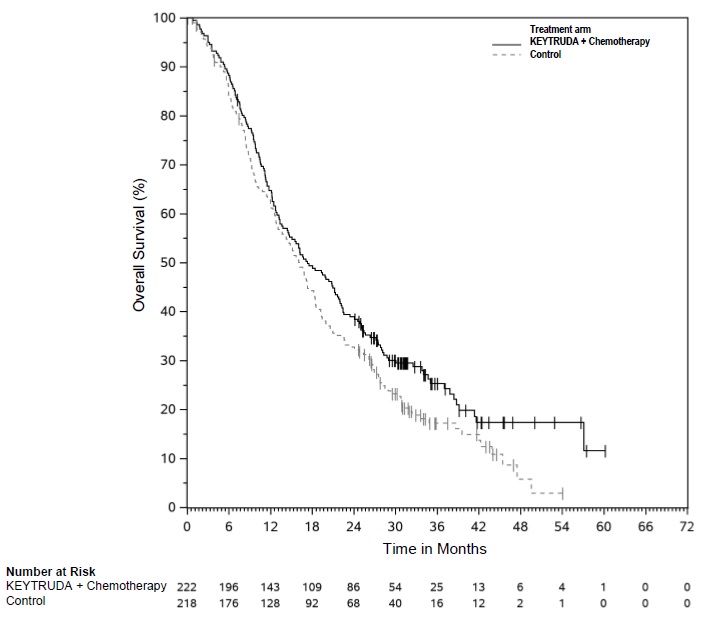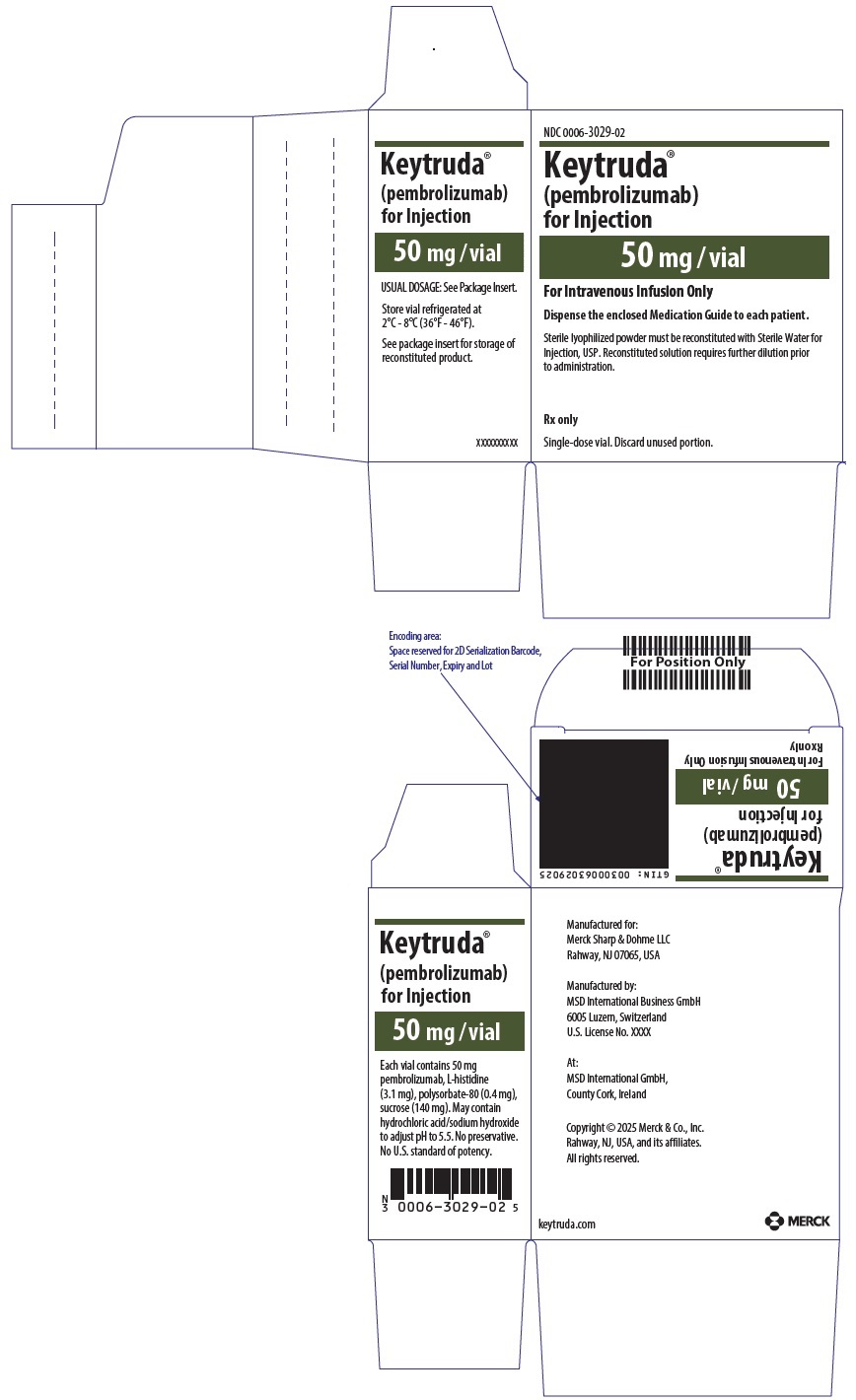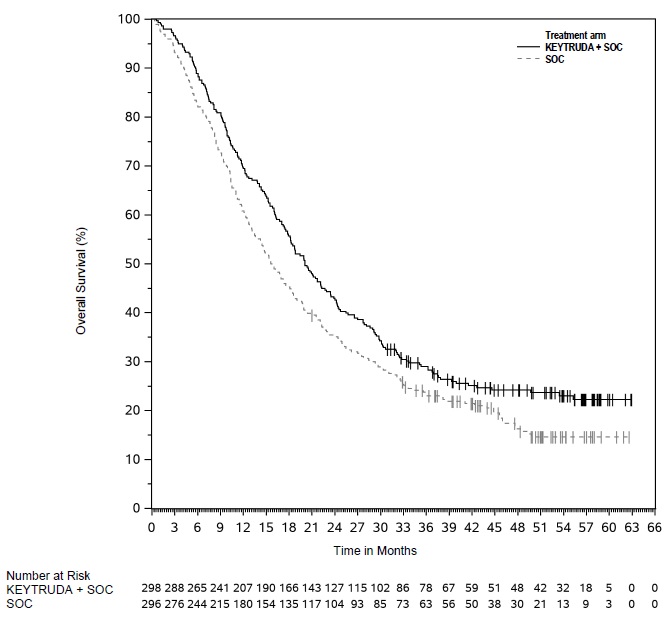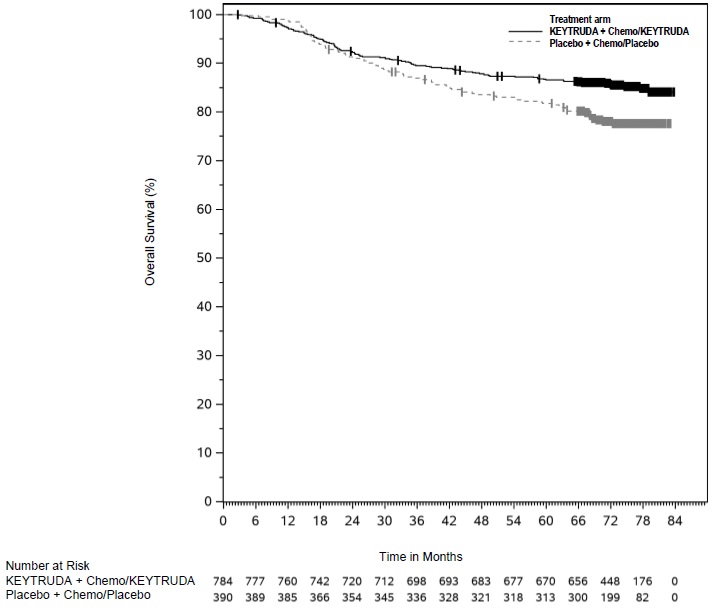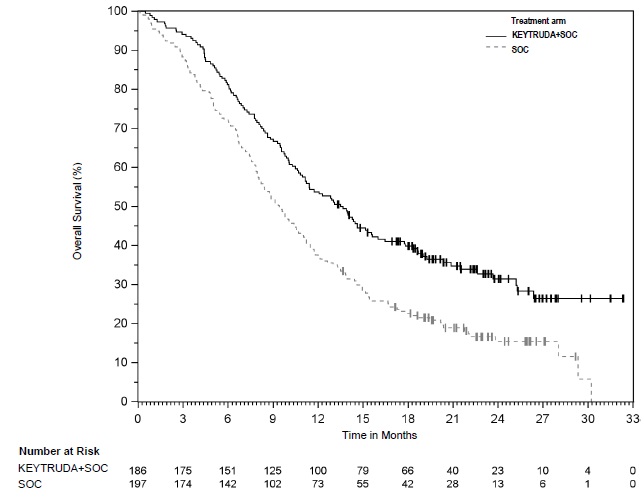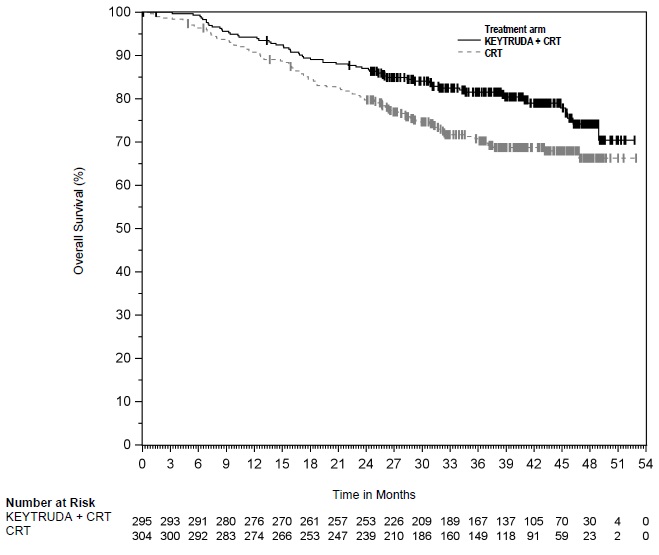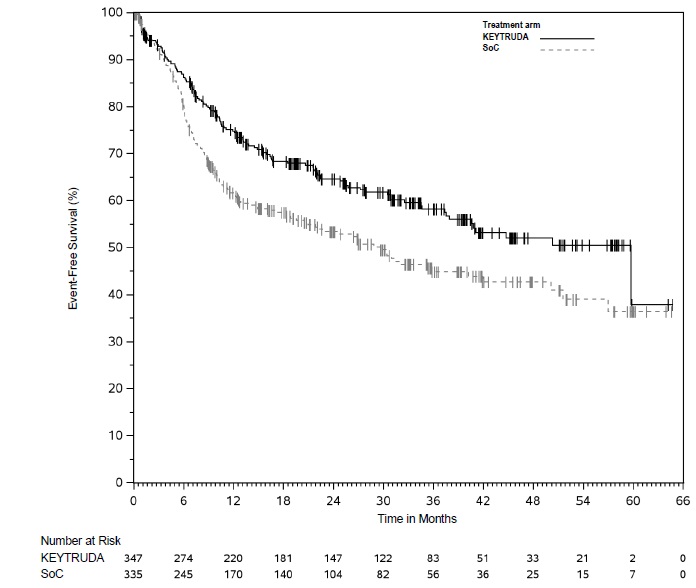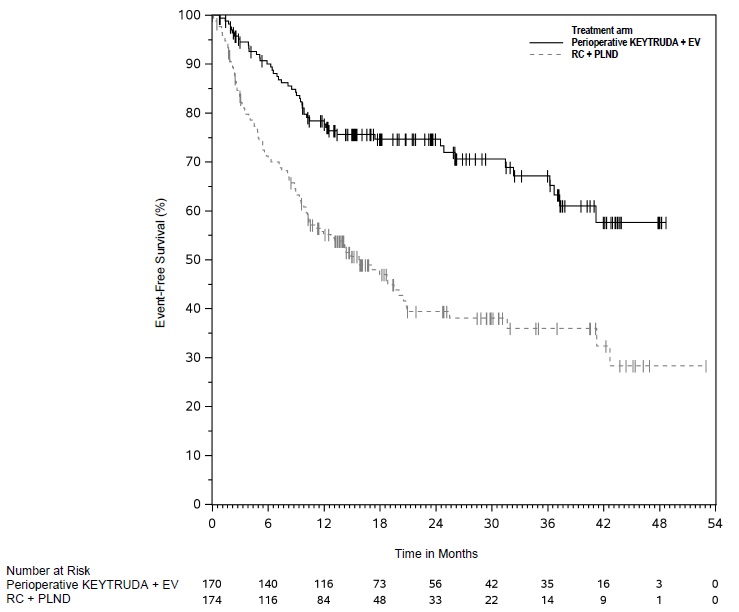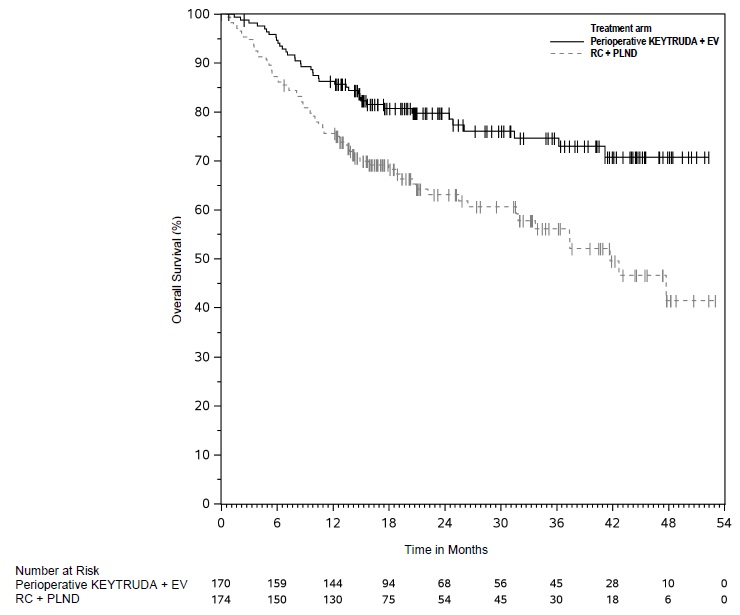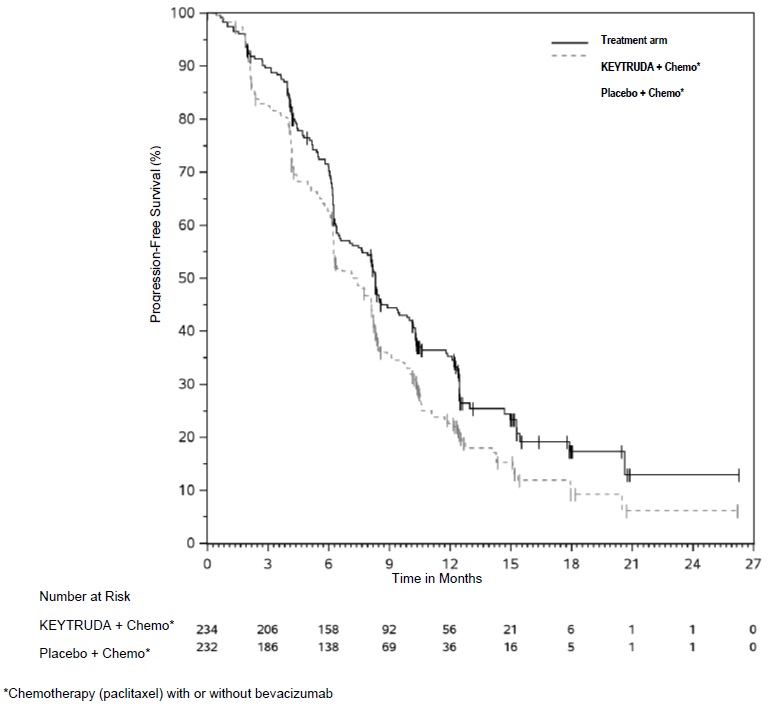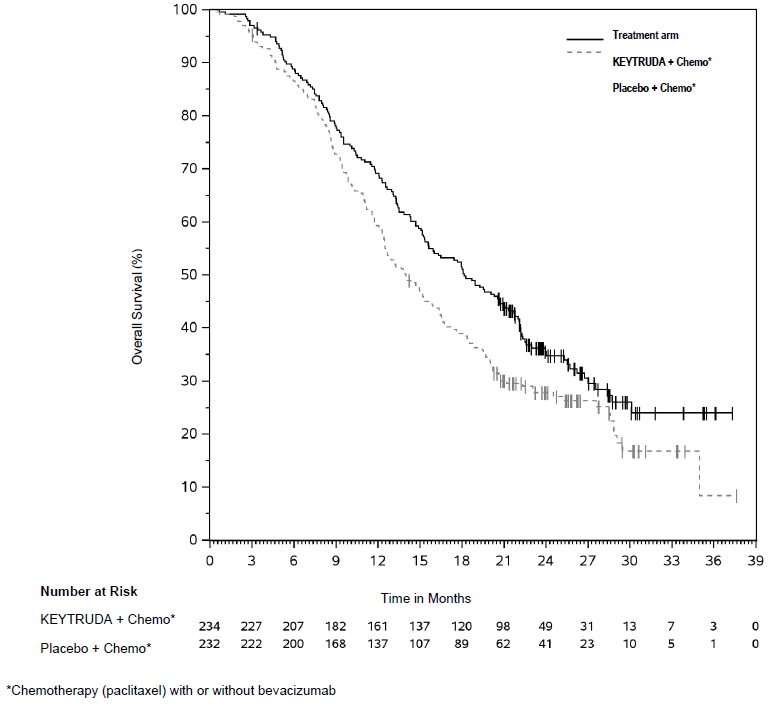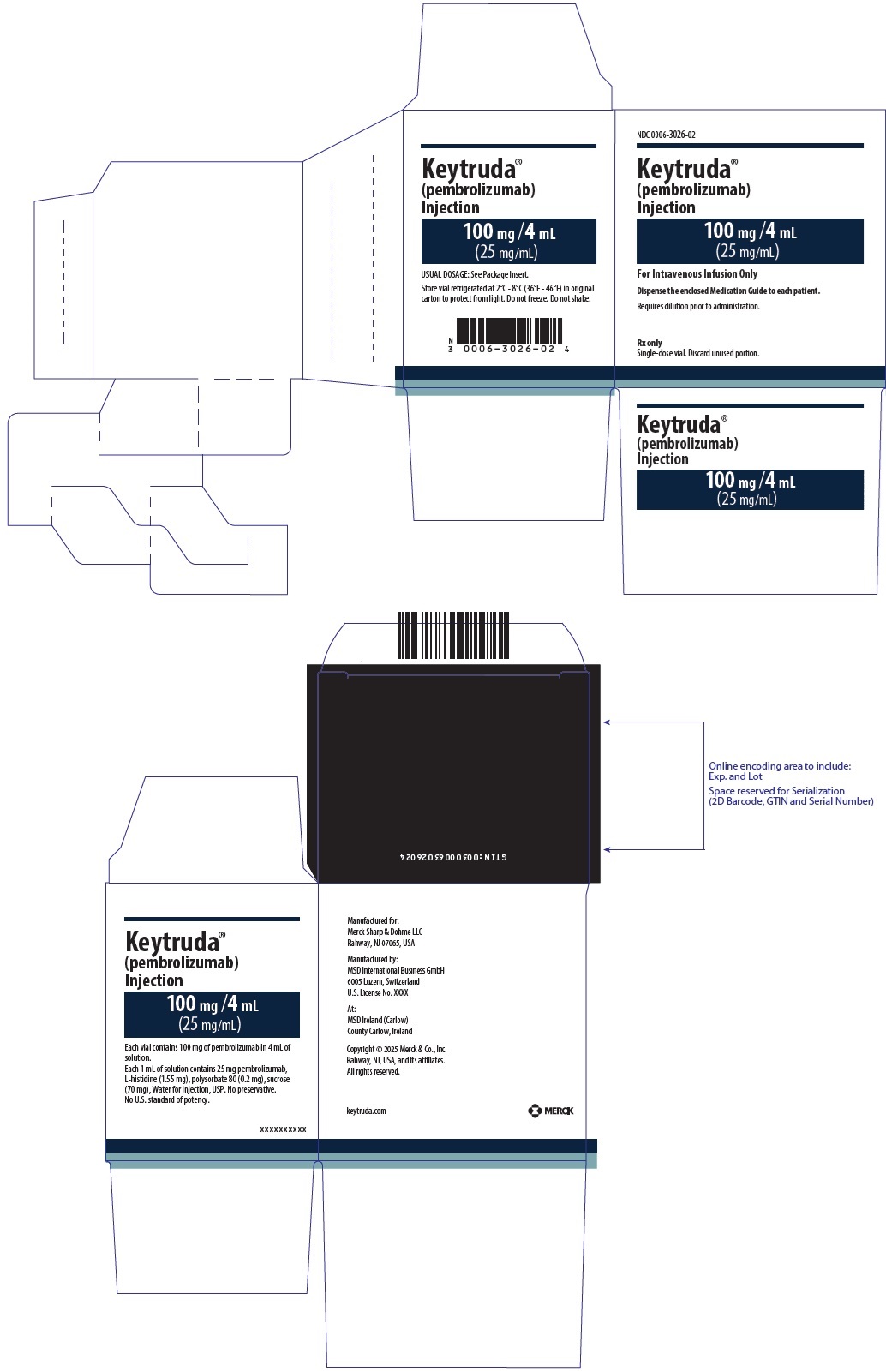 DRUG LABEL: KEYTRUDA
NDC: 0006-3029 | Form: INJECTION, POWDER, LYOPHILIZED, FOR SOLUTION
Manufacturer: Merck Sharp & Dohme LLC 
Category: prescription | Type: HUMAN PRESCRIPTION DRUG LABEL
Date: 20260210

ACTIVE INGREDIENTS: pembrolizumab 50 mg/2 mL
INACTIVE INGREDIENTS: HISTIDINE 3.1 mg/2 mL; SUCROSE 140 mg/2 mL; POLYSORBATE 80 0.4 mg/2 mL; SODIUM HYDROXIDE; HYDROCHLORIC ACID

HIGHLIGHTS OF PRESCRIBING INFORMATION

These highlights do not include all the information needed to use KEYTRUDA safely and effectively. See full prescribing information for KEYTRUDA.
KEYTRUDA® (pembrolizumab) injection, for intravenous use
Initial U.S. Approval: 2014

RECENT MAJOR CHANGES

Indications and Usage (1) | 02/2026
Dosage and Administration (2) | 02/2026

1 INDICATIONS AND USAGE

KEYTRUDA is a programmed death receptor-1 (PD-1)-blocking antibody indicated:

Melanoma

- for the treatment of patients with unresectable or metastatic melanoma. (1.1)
- for the adjuvant treatment of adult and pediatric (12 years and older) patients with Stage IIB, IIC, or III melanoma following complete resection. (1.1)

Non-Small Cell Lung Cancer (NSCLC)

- in combination with pemetrexed and platinum chemotherapy, as first-line treatment of patients with metastatic nonsquamous NSCLC, with no EGFR or ALK genomic tumor aberrations. (1.2)
- in combination with carboplatin and either paclitaxel or paclitaxel protein-bound, as first-line treatment of patients with metastatic squamous NSCLC. (1.2)
- as a single agent for the first-line treatment of patients with NSCLC expressing PD-L1 [Tumor Proportion Score (TPS) ≥1%] as determined by an FDA-authorized test, with no EGFR or ALK genomic tumor aberrations, and is:
  - Stage III where patients are not candidates for surgical resection or definitive chemoradiation, or
  - metastatic. (1.2, 2.1)
- as a single agent for the treatment of patients with metastatic NSCLC whose tumors express PD-L1 (TPS ≥1%) as determined by an FDA-authorized test, with disease progression on or after platinum-containing chemotherapy. Patients with EGFR or ALK genomic tumor aberrations should have disease progression on FDA-approved therapy for these aberrations prior to receiving KEYTRUDA. (1.2, 2.1)
- for the treatment of patients with resectable (tumors ≥4 cm or node positive) NSCLC in combination with platinum-containing chemotherapy as neoadjuvant treatment, and then continued as a single agent as adjuvant treatment after surgery. (1.2)
- as a single agent, for adjuvant treatment following resection and platinum-based chemotherapy for adult patients with Stage IB (T2a ≥4 cm), II, or IIIA NSCLC. (1.2)

Malignant Pleural Mesothelioma (MPM)

- in combination with pemetrexed and platinum chemotherapy, as first-line treatment of adult patients with unresectable advanced or metastatic MPM. (1.3)

Head and Neck Squamous Cell Cancer (HNSCC)

- for the treatment of adult patients with resectable locally advanced HNSCC whose tumors express PD-L1 [Combined Positive Score (CPS) ≥1] as determined by an FDA-authorized test, as a single agent as neoadjuvant treatment, continued as adjuvant treatment in combination with radiotherapy (RT) with or without cisplatin and then as a single agent. (1.4)
- in combination with platinum and FU for the first-line treatment of patients with metastatic or with unresectable, recurrent HNSCC. (1.4)
- as a single agent for the first-line treatment of patients with metastatic or with unresectable, recurrent HNSCC whose tumors express PD-L1 [Combined Positive Score (CPS) ≥1] as determined by an FDA-authorized test. (1.4, 2.1)
- as a single agent for the treatment of patients with recurrent or metastatic HNSCC with disease progression on or after platinum-containing chemotherapy. (1.4)

Classical Hodgkin Lymphoma (cHL)

- for the treatment of adult patients with relapsed or refractory cHL. (1.5)
- for the treatment of pediatric patients with refractory cHL, or cHL that has relapsed after 2 or more lines of therapy. (1.5)

Primary Mediastinal Large B-Cell Lymphoma (PMBCL)

- for the treatment of adult and pediatric patients with refractory PMBCL, or who have relapsed after 2 or more prior lines of therapy. (1.6)
- Limitations of Use: KEYTRUDA is not recommended for treatment of patients with PMBCL who require urgent cytoreductive therapy.

Urothelial Cancer

- in combination with enfortumab vedotin, for the treatment of adult patients with locally advanced or metastatic urothelial cancer. (1.7)
- as a single agent for the treatment of patients with locally advanced or metastatic urothelial carcinoma who:
  - are not eligible for any platinum-containing chemotherapy, or
  - who have disease progression during or following platinum-containing chemotherapy or within 12 months of neoadjuvant or adjuvant treatment with platinum-containing chemotherapy. (1.7)
- in combination with enfortumab vedotin, as neoadjuvant treatment and then continued after cystectomy as adjuvant treatment of adult patients with muscle invasive bladder cancer (MIBC) who are ineligible for cisplatin-containing chemotherapy. (1.7)
- as a single agent for the treatment of patients with Bacillus Calmette-Guerin (BCG)-unresponsive, high-risk, non-muscle invasive bladder cancer (NMIBC) with carcinoma in situ (CIS) with or without papillary tumors who are ineligible for or have elected not to undergo cystectomy. (1.7)

Microsatellite Instability-High or Mismatch Repair Deficient Cancer

- for the treatment of adult and pediatric patients with unresectable or metastatic microsatellite instability-high (MSI-H) or mismatch repair deficient (dMMR) solid tumors, as determined by an FDA-authorized test, that have progressed following prior treatment and who have no satisfactory alternative treatment options. (1.8, 2.1)

Microsatellite Instability-High or Mismatch Repair Deficient Colorectal Cancer (CRC)

- for the treatment of patients with unresectable or metastatic MSI-H or dMMR colorectal cancer (CRC) as determined by an FDA-authorized test. (1.9, 2.1)

Gastric Cancer

- in combination with trastuzumab, fluoropyrimidine- and platinum-containing chemotherapy, for the first-line treatment of adults with locally advanced unresectable or metastatic HER2-positive gastric or gastroesophageal junction (GEJ) adenocarcinoma whose tumors express PD-L1 (CPS ≥1) as determined by an FDA-authorized test. (1.10)
- in combination with fluoropyrimidine- and platinum-containing chemotherapy, for the first-line treatment of adults with locally advanced unresectable or metastatic HER2-negative gastric or gastroesophageal junction (GEJ) adenocarcinoma whose tumors express PD-L1 (CPS ≥1) as determined by an FDA-authorized test. (1.10)

Esophageal Cancer

- for the treatment of patients with locally advanced or metastatic esophageal or gastroesophageal junction (GEJ) (tumors with epicenter 1 to 5 centimeters above the GEJ) carcinoma that is not amenable to surgical resection or definitive chemoradiation either:
  - in combination with platinum- and fluoropyrimidine-based chemotherapy for patients whose tumors express PD-L1 (CPS ≥1), or
  - as a single agent after one or more prior lines of systemic therapy for patients with tumors of squamous cell histology that express PD-L1 (CPS ≥10) as determined by an FDA-authorized test. (1.11, 2.1)

Cervical Cancer

- in combination with chemoradiotherapy, for the treatment of patients with locally advanced cervical cancer involving the lower third of the vagina, with or without extension to pelvic sidewall, or hydronephrosis/non-functioning kidney, or spread to adjacent pelvic organs (FIGO 2014 Stage III-IVA). (1.12)
- in combination with chemotherapy, with or without bevacizumab, for the treatment of patients with persistent, recurrent, or metastatic cervical cancer whose tumors express PD-L1 (CPS ≥1) as determined by an FDA-authorized test. (1.12, 2.1)
- as a single agent for the treatment of patients with recurrent or metastatic cervical cancer with disease progression on or after chemotherapy whose tumors express PD-L1 (CPS ≥1) as determined by an FDA-authorized test. (1.12, 2.1)

Hepatocellular Carcinoma (HCC)

- for the treatment of patients with HCC secondary to hepatitis B who have received prior systemic therapy other than a PD-1/PD-L1-containing regimen. (1.13)

Biliary Tract Cancer (BTC)

- in combination with gemcitabine and cisplatin, for the treatment of patients with locally advanced unresectable or metastatic biliary tract cancer. (1.14)

Merkel Cell Carcinoma (MCC)

- for the treatment of adult and pediatric patients with recurrent locally advanced or metastatic Merkel cell carcinoma. (1.15)

Renal Cell Carcinoma (RCC)

- in combination with axitinib, for the first-line treatment of adult patients with advanced RCC. (1.16)
- in combination with lenvatinib, for the first-line treatment of adult patients with advanced RCC. (1.16)
- for the adjuvant treatment of patients with RCC at intermediate-high or high risk of recurrence following nephrectomy, or following nephrectomy and resection of metastatic lesions. (1.16)

Endometrial Carcinoma

- in combination with carboplatin and paclitaxel, followed by KEYTRUDA as a single agent, for the treatment of adult patients with primary advanced or recurrent endometrial carcinoma. (1.17)
- in combination with lenvatinib, for the treatment of adult patients with advanced endometrial carcinoma that is mismatch repair proficient (pMMR) or not MSI-H as determined by an FDA-authorized test, who have disease progression following prior systemic therapy in any setting and are not candidates for curative surgery or radiation. (1.17, 2.1)
- as a single agent, for the treatment of adult patients with advanced endometrial carcinoma that is MSI-H or dMMR, as determined by an FDA-authorized test, who have disease progression following prior systemic therapy in any setting and are not candidates for curative surgery or radiation. (1.17, 2.1)

Tumor Mutational Burden-High (TMB-H) Cancer

- for the treatment of adult and pediatric patients with unresectable or metastatic tumor mutational burden-high (TMB-H) [≥10 mutations/megabase (mut/Mb)] solid tumors, as determined by an FDA-authorized test, that have progressed following prior treatment and who have no satisfactory alternative treatment options.^1 (1.18, 2.1)
- Limitations of Use: The safety and effectiveness of KEYTRUDA in pediatric patients with TMB-H central nervous system cancers have not been established.

Cutaneous Squamous Cell Carcinoma (cSCC)

- for the treatment of patients with recurrent or metastatic cSCC or locally advanced cSCC that is not curable by surgery or radiation. (1.19)

Triple-Negative Breast Cancer (TNBC)

- for the treatment of patients with high-risk early-stage TNBC in combination with chemotherapy as neoadjuvant treatment, and then continued as a single agent as adjuvant treatment after surgery. (1.20)
- in combination with chemotherapy, for the treatment of patients with locally recurrent unresectable or metastatic TNBC whose tumors express PD-L1 (CPS ≥10) as determined by an FDA-authorized test. (1.20, 2.1)

Ovarian Cancer

- in combination with paclitaxel, with or without bevacizumab, for the treatment of adult patients with platinum-resistant epithelial ovarian, fallopian tube, or primary peritoneal carcinoma whose tumors express PD-L1 (CPS ≥1) as determined by an FDA-authorized test, and who have received one or two prior systemic treatment regimens. (1.21, 2.1)

^1 This indication is approved under accelerated approval based on tumor response rate and durability of response. Continued approval for this indication may be contingent upon verification and description of clinical benefit in the confirmatory trials.

2 DOSAGE AND ADMINISTRATION

- Melanoma: 200 mg every 3 weeks or 400 mg every 6 weeks; 2 mg/kg (up to 200 mg) every 3 weeks for pediatrics. (2.2)
- NSCLC: 200 mg every 3 weeks or 400 mg every 6 weeks. (2.2)
- MPM: 200 mg every 3 weeks or 400 mg every 6 weeks. (2.2)
- HNSCC: 200 mg every 3 weeks or 400 mg every 6 weeks. (2.2)
- cHL or PMBCL: 200 mg every 3 weeks or 400 mg every 6 weeks for adults; 2 mg/kg (up to 200 mg) every 3 weeks for pediatrics. (2.2)
- Urothelial Cancer: 200 mg every 3 weeks or 400 mg every 6 weeks. (2.2)
- MSI-H or dMMR Cancer: 200 mg every 3 weeks or 400 mg every 6 weeks for adults; 2 mg/kg (up to 200 mg) every 3 weeks for pediatrics. (2.2)
- MSI-H or dMMR CRC: 200 mg every 3 weeks or 400 mg every 6 weeks. (2.2)
- Gastric Cancer: 200 mg every 3 weeks or 400 mg every 6 weeks. (2.2)
- Esophageal Cancer: 200 mg every 3 weeks or 400 mg every 6 weeks. (2.2)
- Cervical Cancer: 200 mg every 3 weeks or 400 mg every 6 weeks. (2.2)
- HCC: 200 mg every 3 weeks or 400 mg every 6 weeks. (2.2)
- BTC: 200 mg every 3 weeks or 400 mg every 6 weeks. (2.2)
- MCC: 200 mg every 3 weeks or 400 mg every 6 weeks for adults; 2 mg/kg (up to 200 mg) every 3 weeks for pediatrics. (2.2)
- RCC: 200 mg every 3 weeks or 400 mg every 6 weeks as a single agent in the adjuvant setting, or in the advanced setting with either:
  - axitinib 5 mg orally twice daily or
  - lenvatinib 20 mg orally once daily. (2.2)
- Endometrial Carcinoma: 200 mg every 3 weeks or 400 mg every 6 weeks
  - in combination with carboplatin and paclitaxel regardless of MMR or MSI status, or
  - in combination with lenvatinib 20 mg orally once daily for pMMR or not MSI-H tumors, or
  - as a single agent for MSI-H or dMMR tumors. (2.2)
- TMB-H Cancer: 200 mg every 3 weeks or 400 mg every 6 weeks for adults; 2 mg/kg (up to 200 mg) every 3 weeks for pediatrics. (2.2)
- cSCC: 200 mg every 3 weeks or 400 mg every 6 weeks. (2.2)
- TNBC: 200 mg every 3 weeks or 400 mg every 6 weeks. (2.2)
- Ovarian cancer: 200 mg every 3 weeks or 400 mg every 6 weeks. (2.2)
- Administer KEYTRUDA as an intravenous infusion over 30 minutes after dilution. (2.4)
- See Full Prescribing Information for dosage modifications for adverse reactions and preparation and administration instructions. (2.3, 2.4)

3 DOSAGE FORMS AND STRENGTHS

- Injection: 100 mg/4 mL (25 mg/mL) solution in a single-dose vial (3)

4 CONTRAINDICATIONS

None. (4)

5 WARNINGS AND PRECAUTIONS

- Immune-Mediated Adverse Reactions (5.1)
  - Immune-mediated adverse reactions, which may be severe or fatal, can occur in any organ system or tissue, including the following: immune-mediated pneumonitis, immune-mediated colitis, immune-mediated hepatitis, immune-mediated endocrinopathies, immune-mediated nephritis with renal dysfunction, immune-mediated dermatologic adverse reactions, and solid organ transplant rejection.
  - Monitor for early identification and management. Evaluate liver enzymes, creatinine, and thyroid function at baseline and periodically during treatment.
  - Withhold or permanently discontinue based on severity and type of reaction.
- Infusion-related reactions: Interrupt, slow the rate of infusion, or permanently discontinue KEYTRUDA based on the severity of reaction. (5.2)
- Complications of allogeneic HSCT: Fatal and other serious complications can occur in patients who receive allogeneic HSCT before or after being treated with a PD-1/PD-L1 blocking antibody. (5.3)
- Treatment of patients with multiple myeloma with a PD-1 or PD-L1 blocking antibody in combination with a thalidomide analogue plus dexamethasone is not recommended outside of controlled clinical trials. (5.4)
- Embryo-Fetal toxicity: Can cause fetal harm. Advise females of reproductive potential of the potential risk to a fetus and to use effective method of contraception. (5.5, 8.1, 8.3)

6 ADVERSE REACTIONS

Most common adverse reactions (reported in ≥20% of patients) were:

- KEYTRUDA as a single agent: fatigue, musculoskeletal pain, rash, diarrhea, pyrexia, cough, decreased appetite, pruritus, dyspnea, constipation, pain, abdominal pain, nausea, and hypothyroidism. (6.1)
- KEYTRUDA in combination with chemotherapy or chemoradiotherapy: fatigue/asthenia, nausea, constipation, diarrhea, decreased appetite, rash, vomiting, cough, dyspnea, pyrexia, alopecia, peripheral neuropathy, mucosal inflammation, stomatitis, headache, weight loss, abdominal pain, arthralgia, myalgia, insomnia, palmar-plantar erythrodysesthesia, urinary tract infection, hypothyroidism, radiation skin injury, dysphagia, dry mouth, and musculoskeletal pain. (6.1)
- KEYTRUDA in combination with chemotherapy and bevacizumab: peripheral neuropathy, alopecia, anemia, fatigue/asthenia, nausea, neutropenia, diarrhea, hypertension, thrombocytopenia, constipation, arthralgia, vomiting, urinary tract infection, rash, leukopenia, hypothyroidism, decreased appetite, pyrexia, epistaxis, decreased white blood cell count, and stomatitis. (6.1)
- KEYTRUDA in combination with axitinib: diarrhea, fatigue/asthenia, hypertension, hepatotoxicity, hypothyroidism, decreased appetite, palmar-plantar erythrodysesthesia, nausea, stomatitis/mucosal inflammation, dysphonia, rash, cough, and constipation. (6.1)
- KEYTRUDA in combination with lenvatinib: hypothyroidism, hypertension, fatigue, diarrhea, musculoskeletal disorders, nausea, decreased appetite, vomiting, stomatitis, weight loss, abdominal pain, urinary tract infection, proteinuria, constipation, headache, hemorrhagic events, palmar-plantar erythrodysesthesia, dysphonia, rash, hepatotoxicity, and acute kidney injury. (6.1)
- KEYTRUDA in combination with enfortumab vedotin: rash, peripheral neuropathy, fatigue, pruritus, diarrhea, alopecia, weight loss, decreased appetite, dry eye, nausea, constipation, dysgeusia, and urinary tract infection. (6.1)

To report SUSPECTED ADVERSE REACTIONS, contact Merck Sharp & Dohme LLC at 1-877-888-4231 or FDA at 1-800-FDA-1088 or www.fda.gov/medwatch.

8 USE IN SPECIFIC POPULATIONS

Lactation: Advise not to breastfeed. (8.2)

FULL PRESCRIBING INFORMATION

1 INDICATIONS AND USAGE

1.1 Melanoma

KEYTRUDA® is indicated for the treatment of patients with unresectable or metastatic melanoma.

KEYTRUDA is indicated for the adjuvant treatment of adult and pediatric (12 years and older) patients with Stage IIB, IIC, or III melanoma following complete resection.

1.2 Non-Small Cell Lung Cancer

KEYTRUDA, in combination with pemetrexed and platinum chemotherapy, is indicated for the first-line treatment of patients with metastatic nonsquamous non-small cell lung cancer (NSCLC), with no EGFR or ALK genomic tumor aberrations.

KEYTRUDA, in combination with carboplatin and either paclitaxel or paclitaxel protein-bound, is indicated for the first-line treatment of patients with metastatic squamous NSCLC.

KEYTRUDA, as a single agent, is indicated for the first-line treatment of patients with NSCLC expressing PD-L1 [Tumor Proportion Score (TPS) ≥1%] as determined by an FDA-authorized test [see Dosage and Administration (2.1)], with no EGFR or ALK genomic tumor aberrations, and is:

- Stage III where patients are not candidates for surgical resection or definitive chemoradiation, or
- metastatic.

KEYTRUDA, as a single agent, is indicated for the treatment of patients with metastatic NSCLC whose tumors express PD-L1 (TPS ≥1%) as determined by an FDA-authorized test [see Dosage and Administration (2.1)], with disease progression on or after platinum-containing chemotherapy. Patients with EGFR or ALK genomic tumor aberrations should have disease progression on FDA-approved therapy for these aberrations prior to receiving KEYTRUDA.

KEYTRUDA is indicated for the treatment of patients with resectable (tumors ≥4 cm or node positive) NSCLC in combination with platinum-containing chemotherapy as neoadjuvant treatment, and then continued as a single agent as adjuvant treatment after surgery.

KEYTRUDA, as a single agent, is indicated as adjuvant treatment following resection and platinum-based chemotherapy for adult patients with Stage IB (T2a ≥4 cm), II, or IIIA NSCLC.

1.3 Malignant Pleural Mesothelioma

KEYTRUDA, in combination with pemetrexed and platinum chemotherapy, is indicated for the first-line treatment of adult patients with unresectable advanced or metastatic malignant pleural mesothelioma (MPM).

1.4 Head and Neck Squamous Cell Cancer

KEYTRUDA is indicated for the treatment of adult patients with resectable locally advanced HNSCC whose tumors express PD-L1 [Combined Positive Score (CPS) ≥1] as determined by an FDA-authorized test [see Dosage and Administration (2.1)], as a single agent as neoadjuvant treatment, continued as adjuvant treatment in combination with radiotherapy (RT) with or without cisplatin and then as a single agent.

KEYTRUDA, in combination with platinum and fluorouracil (FU), is indicated for the first-line treatment of patients with metastatic or with unresectable, recurrent head and neck squamous cell carcinoma (HNSCC).

KEYTRUDA, as a single agent, is indicated for the first-line treatment of patients with metastatic or with unresectable, recurrent HNSCC whose tumors express PD-L1 [Combined Positive Score (CPS) ≥1] as determined by an FDA-authorized test [see Dosage and Administration (2.1)].

KEYTRUDA, as a single agent, is indicated for the treatment of patients with recurrent or metastatic HNSCC with disease progression on or after platinum-containing chemotherapy.

1.5 Classical Hodgkin Lymphoma

KEYTRUDA is indicated for the treatment of adult patients with relapsed or refractory classical Hodgkin lymphoma (cHL).

KEYTRUDA is indicated for the treatment of pediatric patients with refractory cHL, or cHL that has relapsed after 2 or more lines of therapy.

1.6 Primary Mediastinal Large B-Cell Lymphoma

KEYTRUDA is indicated for the treatment of adult and pediatric patients with refractory primary mediastinal large B-cell lymphoma (PMBCL), or who have relapsed after 2 or more prior lines of therapy.

Limitations of Use: KEYTRUDA is not recommended for treatment of patients with PMBCL who require urgent cytoreductive therapy.

1.7 Urothelial Cancer

KEYTRUDA, in combination with enfortumab vedotin, is indicated for the treatment of adult patients with locally advanced or metastatic urothelial cancer.

KEYTRUDA, as a single agent, is indicated for the treatment of patients with locally advanced or metastatic urothelial carcinoma:

- who are not eligible for any platinum-containing chemotherapy, or
- who have disease progression during or following platinum-containing chemotherapy or within 12 months of neoadjuvant or adjuvant treatment with platinum-containing chemotherapy.

KEYTRUDA, in combination with enfortumab vedotin, as neoadjuvant treatment and then continued after cystectomy as adjuvant treatment, is indicated for the treatment of adult patients with muscle invasive bladder cancer (MIBC) who are ineligible for cisplatin-containing chemotherapy.

KEYTRUDA, as a single agent, is indicated for the treatment of patients with Bacillus Calmette-Guerin (BCG)-unresponsive, high-risk, non-muscle invasive bladder cancer (NMIBC) with carcinoma in situ (CIS) with or without papillary tumors who are ineligible for or have elected not to undergo cystectomy.

1.8 Microsatellite Instability-High or Mismatch Repair Deficient Cancer

KEYTRUDA is indicated for the treatment of adult and pediatric patients with unresectable or metastatic microsatellite instability-high (MSI-H) or mismatch repair deficient (dMMR) solid tumors, as determined by an FDA-authorized test, that have progressed following prior treatment and who have no satisfactory alternative treatment options [see Dosage and Administration (2.1)].

1.9 Microsatellite Instability-High or Mismatch Repair Deficient Colorectal Cancer

KEYTRUDA is indicated for the treatment of patients with unresectable or metastatic MSI-H or dMMR colorectal cancer (CRC) as determined by an FDA-authorized test [see Dosage and Administration (2.1)].

1.10 Gastric Cancer

KEYTRUDA, in combination with trastuzumab, fluoropyrimidine- and platinum-containing chemotherapy, is indicated for the first-line treatment of adults with locally advanced unresectable or metastatic HER2-positive gastric or gastroesophageal junction (GEJ) adenocarcinoma whose tumors express PD-L1 (CPS ≥1) as determined by an FDA-authorized test [see Dosage and Administration (2.1)].

KEYTRUDA, in combination with fluoropyrimidine- and platinum-containing chemotherapy, is indicated for the first-line treatment of adults with locally advanced unresectable or metastatic HER2-negative gastric or gastroesophageal junction (GEJ) adenocarcinoma whose tumors express PD-L1 (CPS ≥ 1) as determined by an FDA-authorized test [see Dosage and Administration (2.1)].

1.11 Esophageal Cancer

KEYTRUDA is indicated for the treatment of patients with locally advanced or metastatic esophageal or gastroesophageal junction (GEJ) (tumors with epicenter 1 to 5 centimeters above the GEJ) carcinoma that is not amenable to surgical resection or definitive chemoradiation either:

- in combination with platinum- and fluoropyrimidine-based chemotherapy for patients with tumors that express PD-L1 (CPS ≥ 1) [see Dosage and Administration (2.1)], or
- as a single agent after one or more prior lines of systemic therapy for patients with tumors of squamous cell histology that express PD-L1 (CPS ≥10) as determined by an FDA-authorized test [see Dosage and Administration (2.1)].

1.12 Cervical Cancer

KEYTRUDA, in combination with chemoradiotherapy (CRT), is indicated for the treatment of patients with locally advanced cervical cancer involving the lower third of the vagina, with or without extension to pelvic sidewall, or hydronephrosis/non-functioning kidney, or spread to adjacent pelvic organs (FIGO 2014 Stage III-IVA).

KEYTRUDA, in combination with chemotherapy, with or without bevacizumab, is indicated for the treatment of patients with persistent, recurrent, or metastatic cervical cancer whose tumors express PD-L1 (CPS ≥1) as determined by an FDA-authorized test [see Dosage and Administration (2.1)].

KEYTRUDA, as a single agent, is indicated for the treatment of patients with recurrent or metastatic cervical cancer with disease progression on or after chemotherapy whose tumors express PD-L1 (CPS ≥1) as determined by an FDA-authorized test [see Dosage and Administration (2.1)].

1.13 Hepatocellular Carcinoma

KEYTRUDA is indicated for the treatment of patients with hepatocellular carcinoma (HCC) secondary to hepatitis B who have received prior systemic therapy other than a PD-1/PD-L1-containing regimen.

1.14 Biliary Tract Cancer

KEYTRUDA, in combination with gemcitabine and cisplatin, is indicated for the treatment of patients with locally advanced unresectable or metastatic biliary tract cancer (BTC).

1.15 Merkel Cell Carcinoma

KEYTRUDA is indicated for the treatment of adult and pediatric patients with recurrent locally advanced or metastatic Merkel cell carcinoma (MCC).

1.16 Renal Cell Carcinoma

KEYTRUDA, in combination with axitinib, is indicated for the first-line treatment of adult patients with advanced renal cell carcinoma (RCC).

KEYTRUDA, in combination with lenvatinib, is indicated for the first-line treatment of adult patients with advanced RCC.

KEYTRUDA is indicated for the adjuvant treatment of patients with RCC at intermediate-high or high risk of recurrence following nephrectomy, or following nephrectomy and resection of metastatic lesions [see Clinical Studies (14.16)].

1.17 Endometrial Carcinoma

KEYTRUDA, in combination with carboplatin and paclitaxel, followed by KEYTRUDA as a single agent, is indicated for the treatment of adult patients with primary advanced or recurrent endometrial carcinoma.

KEYTRUDA, in combination with lenvatinib, is indicated for the treatment of adult patients with advanced endometrial carcinoma that is mismatch repair proficient (pMMR) or not MSI-H as determined by an FDA-authorized test, who have disease progression following prior systemic therapy in any setting and are not candidates for curative surgery or radiation [see Dosage and Administration (2.1)].

KEYTRUDA, as a single agent, is indicated for the treatment of adult patients with advanced endometrial carcinoma that is MSI-H or dMMR, as determined by an FDA-authorized test, who have disease progression following prior systemic therapy in any setting and are not candidates for curative surgery or radiation [see Dosage and Administration (2.1)].

1.18 Tumor Mutational Burden-High Cancer

KEYTRUDA is indicated for the treatment of adult and pediatric patients with unresectable or metastatic tumor mutational burden-high (TMB-H) [≥10 mutations/megabase (mut/Mb)] solid tumors, as determined by an FDA-authorized test [see Dosage and Administration (2.1)], that have progressed following prior treatment and who have no satisfactory alternative treatment options.

This indication is approved under accelerated approval based on tumor response rate and durability of response [see Clinical Studies (14.18)]. Continued approval for this indication may be contingent upon verification and description of clinical benefit in the confirmatory trials.

Limitations of Use: The safety and effectiveness of KEYTRUDA in pediatric patients with TMB-H central nervous system cancers have not been established.

1.19 Cutaneous Squamous Cell Carcinoma

KEYTRUDA is indicated for the treatment of patients with recurrent or metastatic cutaneous squamous cell carcinoma (cSCC) or locally advanced cSCC that is not curable by surgery or radiation.

1.20 Triple-Negative Breast Cancer

KEYTRUDA is indicated for the treatment of patients with high-risk early-stage triple-negative breast cancer (TNBC) in combination with chemotherapy as neoadjuvant treatment, and then continued as a single agent as adjuvant treatment after surgery.

KEYTRUDA, in combination with chemotherapy, is indicated for the treatment of patients with locally recurrent unresectable or metastatic TNBC whose tumors express PD-L1 (CPS ≥10) as determined by an FDA-authorized test [see Dosage and Administration (2.1)].

1.21 Ovarian Cancer

KEYTRUDA, in combination with paclitaxel, with or without bevacizumab, is indicated for the treatment of adult patients with platinum-resistant epithelial ovarian, fallopian tube, or primary peritoneal carcinoma whose tumors express PD-L1 (CPS ≥1) as determined by an FDA-authorized test [see Dosage and Administration (2.1)], and who have received one or two prior systemic treatment regimens.

2 DOSAGE AND ADMINISTRATION

2.1 Patient Selection

Information on FDA-authorized tests for patient selection is available at:

http://www.fda.gov/CompanionDiagnostics.

Patient Selection for Single-Agent Treatment

Select patients for treatment with KEYTRUDA as a single agent based on the presence of positive PD-L1 expression in:

- Stage III NSCLC who are not candidates for surgical resection or definitive chemoradiation [see Clinical Studies (14.2)].
- metastatic NSCLC [see Clinical Studies (14.2)].
- first-line treatment of metastatic or unresectable, recurrent HNSCC [see Clinical Studies (14.4)].
- previously treated recurrent locally advanced or metastatic esophageal cancer [see Clinical Studies (14.11)].
- recurrent or metastatic cervical cancer with disease progression on or after chemotherapy [see Clinical Studies (14.12)].

For the MSI-H/dMMR indications, select patients for treatment with KEYTRUDA as a single agent based on MSI-H/dMMR status in tumor specimens [see Clinical Studies (14.8, 14.9)].

For the TMB-H indication, select patients for treatment with KEYTRUDA as a single agent based on TMB-H status in tumor specimens [see Clinical Studies (14.18)].

Because subclonal dMMR mutations and microsatellite instability may arise in high-grade gliomas during temozolomide therapy, it is recommended to test for TMB-H, MSI-H, and dMMR in the primary tumor specimens obtained prior to initiation of temozolomide chemotherapy in patients with high-grade gliomas.

Additional Patient Selection Information for MSI-H or dMMR in Patients with non-CRC Solid Tumors

Due to discordance between local tests and FDA-authorized tests, confirmation of MSI-H or dMMR status is recommended by an FDA-authorized test in patients with MSI-H or dMMR solid tumors, if feasible. If unable to perform confirmatory MSI-H/dMMR testing, the presence of TMB ≥10 mut/Mb, as determined by an FDA-authorized test, may be used to select patients for treatment [see Clinical Studies (14.8)].

Patient Selection for Combination Therapy

For use of KEYTRUDA as a single agent as neoadjuvant treatment, then in combination with radiotherapy (RT) with or without chemotherapy then continued as a single agent as adjuvant treatment, select patients based on presence of positive PD-L1 expression (CPS ≥1) in resectable locally advanced HNSCC [see Clinical Studies (14.4)].

For use of KEYTRUDA in combination with chemotherapy, select patients based on the presence of positive PD-L1 expression (CPS ≥1) in locally advanced unresectable or metastatic gastric or gastroesophageal junction (GEJ) adenocarcinoma, and esophageal or gastroesophageal junction (GEJ) carcinoma [see Clinical Studies (14.10), (14.11)].

- An FDA-authorized test for the detection of PD-L1 for the selection of patients with PD-L1 (CPS ≥ 1) expression in esophageal carcinoma in combination with platinum- and fluoropyrimidine-based chemotherapy is not available.

For use of KEYTRUDA in combination with chemotherapy, with or without bevacizumab, select patients based on the presence of positive PD-L1 expression in persistent, recurrent, or metastatic cervical cancer [see Clinical Studies (14.12)].

For the pMMR/not MSI-H advanced endometrial carcinoma indication, select patients for treatment with KEYTRUDA in combination with lenvatinib based on MMR or MSI status in tumor specimens [see Clinical Studies (14.17)].

For use of KEYTRUDA in combination with chemotherapy, select patients based on the presence of positive PD-L1 expression in locally recurrent unresectable or metastatic TNBC [see Clinical Studies (14.20)].

For use of KEYTRUDA in combination with paclitaxel, with or without bevacizumab, select patients based on the presence of positive PD-L1 expression (CPS ≥1) in platinum-resistant epithelial ovarian, fallopian tube, or primary peritoneal carcinoma [see Clinical Studies (14.21)].

2.2 Recommended Dosage

Administer KEYTRUDA as a 30-minute intravenous infusion. The recommended dosages of KEYTRUDA are presented in Table 1.

Table 1: Recommended Dosage
Indication | Recommended Dosage of KEYTRUDA | Duration/Timing of Treatment
Monotherapy
Adult patients with unresectable or metastatic melanoma | 200 mg every 3 weeks or 400 mg every 6 weeks | Until disease progression or unacceptable toxicity
Adjuvant treatment of adult patients with melanoma, NSCLC, or RCC | 200 mg every 3 weeks or 400 mg every 6 weeks | Until disease recurrence, unacceptable toxicity, or up to 12 months
Adult patients with NSCLC, HNSCC, cHL, PMBCL, locally advanced or metastatic Urothelial Carcinoma, MSI-H or dMMR Cancer, MSI-H or dMMR CRC, MSI-H or dMMR Endometrial Carcinoma, Esophageal Cancer, Cervical Cancer, HCC, MCC, TMB-H Cancer, or cSCC | 200 mg every 3 weeks or 400 mg every 6 weeks | Until disease progression, unacceptable toxicity, or up to 24 months
Adult patients with high-risk BCG- unresponsive NMIBC | 200 mg every 3 weeks or 400 mg every 6 weeks | Until persistent or recurrent high-risk NMIBC, disease progression, unacceptable toxicity, or up to 24 months
Pediatric patients with cHL, PMBCL, MSI-H or dMMR Cancer, MCC, or TMB- H Cancer | 2 mg/kg every 3 weeks (up to a maximum of 200 mg) | Until disease progression, unacceptable toxicity, or up to 24 months
Pediatric patients (12 years and older) for adjuvant treatment of melanoma | 2 mg/kg every 3 weeks (up to a maximum of 200 mg) | Until disease recurrence, unacceptable toxicity, or up to 12 months
Combination Therapy [Refer to the Prescribing Information for the agents administered in combination with KEYTRUDA for recommended dosing information, as appropriate.]
Adult patients with resectable NSCLC | 200 mg every 3 weeks or 400 mg every 6 weeks Administer KEYTRUDA prior to chemotherapy when given on the same day. | Neoadjuvant treatment in combination with chemotherapy for 12 weeks or until disease progression that precludes definitive surgery or unacceptable toxicity, followed by adjuvant treatment with KEYTRUDA as a single agent after surgery for 39 weeks or until disease recurrence or unacceptable toxicity
Adult patients with NSCLC, MPM, HNSCC, HER2-negative Gastric Cancer, Esophageal Cancer, or BTC | 200 mg every 3 weeks or 400 mg every 6 weeks Administer KEYTRUDA prior to chemotherapy when given on the same day. | Until disease progression, unacceptable toxicity, or up to 24 months
Adult patients with locally advanced or metastatic urothelial cancer | 200 mg every 3 weeks or 400 mg every 6 weeks Administer KEYTRUDA after enfortumab vedotin when given on the same day. | Until disease progression, unacceptable toxicity, or up to 24 months
Adult patients with MIBC | 200 mg every 3 weeks (neoadjuvant) 200mg every 3 weeks or 400 mg every 6 weeks (adjuvant) Administer KEYTRUDA after enfortumab vedotin when given on the same day. | Neoadjuvant:; - Administer KEYTRUDA 200 mg every 3 weeks for 3 doses in combination with enfortumab vedotin or until disease progression that precludes curative-intent cystectomy or unacceptable toxicity.; Adjuvant:; - Administer KEYTRUDA 200 mg every 3 weeks for 14 doses or 400 mg every 6 weeks for 7 doses in combination with enfortumab vedotin or until disease recurrence or unacceptable toxicity
Adult patients with locally advanced HNSCC | 200 mg every 3 weeks or 400 mg every 6 weeks Administer KEYTRUDA prior to cisplatin when given on the same day. | Neoadjuvant:; - Administer KEYTRUDA for 6 weeks or until disease progression that precludes definitive surgery or unacceptable toxicity.; Adjuvant:; - Administer KEYTRUDA in combination with RT with or without cisplatin. - Continue KEYTRUDA as a single agent. - Continue KEYTRUDA until disease recurrence or unacceptable toxicity or up to one year
Adult patients with HER2-positive Gastric Cancer | 200 mg every 3 weeks or 400 mg every 6 weeks Administer KEYTRUDA prior to trastuzumab and chemotherapy when given on the same day. | Until disease progression, unacceptable toxicity, or up to 24 months
Adult patients with Cervical Cancer | 200 mg every 3 weeks or 400 mg every 6 weeks Administer KEYTRUDA prior to chemoradiotherapy or prior to chemotherapy with or without bevacizumab when given on the same day. | Until disease progression, unacceptable toxicity, or for KEYTRUDA, up to 24 months
Adult patients with RCC | 200 mg every 3 weeks or 400 mg every 6 weeks Administer KEYTRUDA in combination with axitinib 5 mg orally twice daily [When axitinib is used in combination with KEYTRUDA, dose escalation of axitinib above the initial 5 mg dose may be considered at intervals of six weeks or longer.] or Administer KEYTRUDA in combination with lenvatinib 20 mg orally once daily. | Until disease progression, unacceptable toxicity, or for KEYTRUDA, up to 24 months
Adult patients with Endometrial Carcinoma | 200 mg every 3 weeks or 400 mg every 6 weeks Administer KEYTRUDA prior to carboplatin and paclitaxel when given on the same day. or Administer KEYTRUDA in combination with lenvatinib 20 mg orally once daily. | Until disease progression, unacceptable toxicity, or for KEYTRUDA, up to 24 months
Adult patients with high-risk early-stage TNBC | 200 mg every 3 weeks or 400 mg every 6 weeks Administer KEYTRUDA prior to chemotherapy when given on the same day. | Neoadjuvant treatment in combination with chemotherapy for 24 weeks (8 doses of 200 mg every 3 weeks or 4 doses of 400 mg every 6 weeks) or until disease progression or unacceptable toxicity, followed by adjuvant treatment with KEYTRUDA as a single agent for up to 27 weeks (9 doses of 200 mg every 3 weeks or 5 doses of 400 mg every 6 weeks) or until disease recurrence or unacceptable toxicity [Patients who experience disease progression or unacceptable toxicity related to KEYTRUDA with neoadjuvant treatment in combination with chemotherapy should not receive adjuvant single agent KEYTRUDA.]
Adult patients with locally recurrent unresectable or metastatic TNBC | 200 mg every 3 weeks or 400 mg every 6 weeks Administer KEYTRUDA prior to chemotherapy when given on the same day. | Until disease progression, unacceptable toxicity, or up to 24 months
Adult patients with Ovarian Cancer | 200 mg every 3 weeks or 400 mg every 6 weeks Administer KEYTRUDA prior to paclitaxel with or without bevacizumab when given on the same day. | Until disease progression, unacceptable toxicity, or up to 24 months

2.3 Dose Modifications

No dose reduction for KEYTRUDA is recommended. In general, withhold KEYTRUDA for severe (Grade 3) immune-mediated adverse reactions. Permanently discontinue KEYTRUDA for Life-threatening (Grade 4) immune-mediated adverse reactions, recurrent severe (Grade 3) immune-mediated reactions that require systemic immunosuppressive treatment, or an inability to reduce corticosteroid dose to 10 mg or less of prednisone or equivalent per day within 12 weeks of initiating steroids.

Dosage modifications for KEYTRUDA for adverse reactions that require management different from these general guidelines are summarized in Table 2.

Table 2: Recommended Dosage Modifications for Adverse Reactions
Adverse Reaction | Severity [Based on Common Terminology Criteria for Adverse Events (CTCAE), version 4.0] | Dosage Modification
Immune-Mediated Adverse Reactions [see Warnings and Precautions (5.1)]
Pneumonitis | Grade 2 | Withhold [Resume in patients with complete or partial resolution (Grades 0 to 1) after corticosteroid taper. Permanently discontinue if no complete or partial resolution within 12 weeks of initiating steroids or inability to reduce prednisone to 10 mg per day or less (or equivalent) within 12 weeks of initiating steroids.]
Pneumonitis | Grade 3 or 4 | Permanently discontinue
Colitis | Grade 2 or 3 | Withhold
Colitis | Grade 4 | Permanently discontinue
Hepatitis with no tumor involvement of the liver | AST or ALT increases to more than 3 and up to 8 times ULN or Total bilirubin increases to more than 1.5 and up to 3 times ULN | Withhold
For liver enzyme elevations in patients treated with combination therapy with axitinib, see Table 3. | AST or ALT increases to more than 8 times ULN or Total bilirubin increases to more than 3 times ULN | Permanently discontinue
Hepatitis with tumor involvement of the liver [If AST and ALT are less than or equal to ULN at baseline, withhold or permanently discontinue KEYTRUDA based on recommendations for hepatitis with no liver involvement.] | Baseline AST or ALT is more than 1 and up to 3 times ULN and increases to more than 5 and up to 10 times ULN or Baseline AST or ALT is more than 3 and up to 5 times ULN and increases to more than 8 and up to 10 times ULN | Withhold
Hepatitis with tumor involvement of the liver [If AST and ALT are less than or equal to ULN at baseline, withhold or permanently discontinue KEYTRUDA based on recommendations for hepatitis with no liver involvement.] | ALT or AST increases to more than 10 times ULN or Total bilirubin increases to more than 3 times ULN | Permanently discontinue
Endocrinopathies | Grade 3 or 4 | Withhold until clinically stable or permanently discontinue depending on severity
Nephritis with Renal Dysfunction | Grade 2 or 3 increased blood creatinine | Withhold
Nephritis with Renal Dysfunction | Grade 4 increased blood creatinine | Permanently discontinue
Exfoliative Dermatologic Conditions | Suspected SJS, TEN, or DRESS | Withhold
Exfoliative Dermatologic Conditions | Confirmed SJS, TEN, or DRESS | Permanently discontinue
Myocarditis | Grade 2, 3, or 4 | Permanently discontinue
Neurological Toxicities | Grade 2 | Withhold
Neurological Toxicities | Grade 3 or 4 | Permanently discontinue
Hematologic toxicity in patients with cHL or PMBCL | Grade 4 | Withhold until resolution to Grades 0 or 1
Other Adverse Reactions
Infusion-related reactions [see Warnings and Precautions (5.2)] | Grade 1 or 2 | Interrupt or slow the rate of infusion
Infusion-related reactions [see Warnings and Precautions (5.2)] | Grade 3 or 4 | Permanently discontinue
ALT = alanine aminotransferase, AST = aspartate aminotransferase, DRESS = Drug Rash with Eosinophilia and Systemic Symptoms, SJS = Stevens Johnson Syndrome, TEN = toxic epidermal necrolysis, ULN = upper limit normal

The following table represents dosage modifications that are different from those described above for KEYTRUDA or in the Full Prescribing Information for the drug administered in combination.

Table 3: Recommended Specific Dosage Modifications for Adverse Reactions for KEYTRUDA in Combination with Axitinib
Treatment | Adverse Reaction | Severity | Dosage Modification
KEYTRUDA in combination with axitinib | Liver enzyme elevations [Consider corticosteroid therapy] | ALT or AST increases to at least 3 times but less than 10 times ULN without concurrent total bilirubin at least 2 times ULN | Withhold both KEYTRUDA and axitinib until resolution to Grades 0 or 1 [Based on Common Terminology Criteria for Adverse Events (CTCAE), version 4.0. Consider rechallenge with a single drug or sequential rechallenge with both drugs after recovery. If rechallenging with axitinib, consider dose reduction as per the axitinib Prescribing Information.]
KEYTRUDA in combination with axitinib | Liver enzyme elevations [Consider corticosteroid therapy] | ALT or AST increases to more than 3 times ULN with concurrent total bilirubin at least 2 times ULN or ALT or AST ≥10 times ULN | Permanently discontinue both KEYTRUDA and axitinib
ALT = alanine aminotransferase, AST = aspartate aminotransferase, ULN = upper limit normal

Recommended Dose Modifications for Adverse Reactions for KEYTRUDA in Combination with Lenvatinib

When administering KEYTRUDA in combination with lenvatinib, modify the dosage of one or both drugs. Withhold or discontinue KEYTRUDA as shown in Table 2. Refer to lenvatinib prescribing information for additional dose modification information.

2.4 Preparation and Administration

Preparation for Intravenous Infusion

- Visually inspect the solution for particulate matter and discoloration. The solution is clear to slightly opalescent, colorless to slightly yellow. Discard the vial if visible particles are observed.
- Dilute KEYTRUDA injection (solution) prior to intravenous administration.
- Withdraw the required volume from the vial(s) of KEYTRUDA and transfer into an intravenous (IV) bag containing 0.9% Sodium Chloride Injection, USP or 5% Dextrose Injection, USP. Mix diluted solution by gentle inversion. Do not shake. The final concentration of the diluted solution should be between 1 mg/mL to 10 mg/mL.
- Discard any unused portion left in the vial.

Storage of Diluted Solution

The product does not contain a preservative.

Store the diluted solution from the KEYTRUDA 100 mg/4 mL vial either:

- At room temperature (temperatures at or below 25°C) for no more than 6 hours from the time of dilution. This includes room temperature storage of the diluted solution, and the duration of infusion.
- Under refrigeration at 2°C to 8°C (36°F to 46°F) for no more than 96 hours from the time of dilution. If refrigerated, allow the diluted solution to come to room temperature prior to administration. Do not shake.

Discard after 6 hours at room temperature or after 96 hours under refrigeration.

Do not freeze.

Administration

- Administer diluted solution intravenously over 30 minutes through an intravenous line containing a sterile, non-pyrogenic, low-protein binding 0.2 micron to 5 micron in-line or add-on filter.
- Do not co-administer other drugs through the same infusion line.

3 DOSAGE FORMS AND STRENGTHS

- Injection: 100 mg/4 mL (25 mg/mL) clear to slightly opalescent, colorless to slightly yellow solution in a single-dose vial

4 CONTRAINDICATIONS

None.

5 WARNINGS AND PRECAUTIONS

5.1 Severe and Fatal Immune-Mediated Adverse Reactions

KEYTRUDA is a monoclonal antibody that belongs to a class of drugs that bind to either the programmed death-receptor 1 (PD-1) or the PD-ligand 1 (PD-L1), blocking the PD-1/PD-L1 pathway, thereby removing inhibition of the immune response, potentially breaking peripheral tolerance and inducing immune-mediated adverse reactions. Important immune-mediated adverse reactions listed under WARNINGS AND PRECAUTIONS may not include all possible severe and fatal immune-mediated adverse reactions.

Immune-mediated adverse reactions, which may be severe or fatal, can occur in any organ system or tissue and can affect more than one body system simultaneously. Immune-mediated adverse reactions can occur at any time after starting treatment with a PD-1/PD-L1 blocking antibody. While immune-mediated adverse reactions usually manifest during treatment with PD-1/PD-L1 blocking antibodies, immune-mediated adverse reactions can also manifest after discontinuation of PD-1/PD-L1 blocking antibodies.

Early identification and management of immune-mediated adverse reactions are essential to ensure safe use of PD-1/PD-L1 blocking antibodies. Monitor patients closely for symptoms and signs that may be clinical manifestations of underlying immune-mediated adverse reactions. Evaluate liver enzymes, creatinine, and thyroid function at baseline and periodically during treatment. For patients with TNBC treated with KEYTRUDA in the neoadjuvant setting, monitor blood cortisol at baseline, prior to surgery, and as clinically indicated. In cases of suspected immune-mediated adverse reactions, initiate appropriate workup to exclude alternative etiologies, including infection. Institute medical management promptly, including specialty consultation as appropriate.

Withhold or permanently discontinue KEYTRUDA depending on severity [see Dosage and Administration (2.3)]. In general, if KEYTRUDA requires interruption or discontinuation, administer systemic corticosteroid therapy (1 to 2 mg/kg/day prednisone or equivalent) until improvement to Grade 1 or less. Upon improvement to Grade 1 or less, initiate corticosteroid taper and continue to taper over at least 1 month. Consider administration of other systemic immunosuppressants in patients whose immune-mediated adverse reactions are not controlled with corticosteroid therapy.

Toxicity management guidelines for adverse reactions that do not necessarily require systemic steroids (e.g., endocrinopathies and dermatologic reactions) are discussed below.

Immune-Mediated Pneumonitis

KEYTRUDA can cause immune-mediated pneumonitis. The incidence of pneumonitis is higher in patients who have received prior thoracic radiation. Immune-mediated pneumonitis occurred in 3.4% (94/2799) of patients receiving KEYTRUDA, including fatal (0.1%), Grade 4 (0.3%), Grade 3 (0.9%), and Grade 2 (1.3%) adverse reactions. Systemic corticosteroids were required in 67% (63/94) of patients with pneumonitis. Pneumonitis led to permanent discontinuation of KEYTRUDA in 1.3% (36) of patients and withholding of KEYTRUDA in 0.9% (26) of patients. All patients who were withheld reinitiated KEYTRUDA after symptom improvement; of these, 23% had recurrence of pneumonitis. Pneumonitis resolved in 59% of the 94 patients.

In clinical studies enrolling 389 adult patients with cHL who received KEYTRUDA as a single agent, pneumonitis occurred in 31 (8%) patients, including Grades 3-4 pneumonitis in 2.3% of patients. Patients received high-dose corticosteroids for a median duration of 10 days (range: 2 days to 53 months). Pneumonitis rates were similar in patients with and without prior thoracic radiation. Pneumonitis led to discontinuation of KEYTRUDA in 21 (5.4%) patients. Of the patients who developed pneumonitis, 42% interrupted KEYTRUDA, 68% discontinued KEYTRUDA, and 77% had resolution.

In a clinical study enrolling 580 adult patients with resected NSCLC (KEYNOTE-091) who received KEYTRUDA as a single agent for adjuvant treatment, pneumonitis occurred in 41 (7%) patients, including fatal (0.2%), Grade 4 (0.3%), and Grade 3 (1%) adverse reactions. Patients received high-dose corticosteroids for a median duration of 10 days (range: 1 day to 2.3 months). Pneumonitis led to discontinuation of KEYTRUDA in 26 (4.5%) of patients. Of the patients who developed pneumonitis, 54% interrupted KEYTRUDA, 63% discontinued KEYTRUDA, and 71% had resolution.

Immune-Mediated Colitis

KEYTRUDA can cause immune-mediated colitis, which may present with diarrhea. Cytomegalovirus (CMV) infection/reactivation has been reported in patients with corticosteroid-refractory immune-mediated colitis. In cases of corticosteroid-refractory colitis, consider repeating infectious workup to exclude alternative etiologies. Immune-mediated colitis occurred in 1.7% (48/2799) of patients receiving KEYTRUDA, including Grade 4 (<0.1%), Grade 3 (1.1%), and Grade 2 (0.4%) adverse reactions. Systemic corticosteroids were required in 69% (33/48) of patients with colitis. Additional immunosuppressant therapy was required in 4.2% of patients. Colitis led to permanent discontinuation of KEYTRUDA in 0.5% (15) of patients and withholding of KEYTRUDA in 0.5% (13) of patients. All patients who were withheld reinitiated KEYTRUDA after symptom improvement; of these, 23% had recurrence of colitis. Colitis resolved in 85% of the 48 patients.

Hepatotoxicity and Immune-Mediated Hepatitis

KEYTRUDA as a Single Agent

KEYTRUDA can cause immune-mediated hepatitis. Immune-mediated hepatitis occurred in 0.7% (19/2799) of patients receiving KEYTRUDA, including Grade 4 (<0.1%), Grade 3 (0.4%), and Grade 2 (0.1%) adverse reactions. Systemic corticosteroids were required in 68% (13/19) of patients with hepatitis. Eleven percent of these patients required additional immunosuppressant therapy. Hepatitis led to permanent discontinuation of KEYTRUDA in 0.2% (6) of patients and withholding of KEYTRUDA in 0.3% (9) of patients. All patients who were withheld reinitiated KEYTRUDA after symptom improvement; of these, none had recurrence of hepatitis. Hepatitis resolved in 79% of the 19 patients.

KEYTRUDA with Axitinib

KEYTRUDA in combination with axitinib can cause hepatic toxicity with higher than expected frequencies of Grades 3 and 4 ALT and AST elevations compared to KEYTRUDA alone. Monitor liver enzymes before initiation of and periodically throughout treatment. Consider more frequent monitoring of liver enzymes as compared to when the drugs are administered as single agents. For elevated liver enzymes, interrupt KEYTRUDA and axitinib, and consider administering corticosteroids as needed [see Dosage and Administration (2.3)].

With the combination of KEYTRUDA and axitinib, Grades 3 and 4 increased ALT (20%) and increased AST (13%) were seen. Fifty-nine percent of the patients with increased ALT received systemic corticosteroids. In patients with ALT ≥3 times ULN (Grades 2-4, n=116), ALT resolved to Grades 0-1 in 94%. Among the 92 patients who were rechallenged with either KEYTRUDA (n=3) or axitinib (n=34) administered as a single agent or with both (n=55), recurrence of ALT ≥3 times ULN was observed in 1 patient receiving KEYTRUDA, 16 patients receiving axitinib, and 24 patients receiving both KEYTRUDA and axitinib. All patients with a recurrence of ALT ≥3 ULN subsequently recovered from the event.

Immune-Mediated Endocrinopathies

Adrenal Insufficiency

KEYTRUDA can cause primary or secondary adrenal insufficiency. For Grade 2 or higher adrenal insufficiency, initiate symptomatic treatment, including hormone replacement as clinically indicated. Withhold KEYTRUDA depending on severity [see Dosage and Administration (2.3)].

Adrenal insufficiency occurred in 0.8% (22/2799) of patients receiving KEYTRUDA, including Grade 4 (<0.1%), Grade 3 (0.3%), and Grade 2 (0.3%) adverse reactions. Systemic corticosteroids were required in 77% (17/22) of patients with adrenal insufficiency; of these, the majority remained on systemic corticosteroids. Adrenal insufficiency led to permanent discontinuation of KEYTRUDA in <0.1% (1) of patients and withholding of KEYTRUDA in 0.3% (8) of patients. All patients who were withheld reinitiated KEYTRUDA after symptom improvement.

Hypophysitis

KEYTRUDA can cause immune-mediated hypophysitis. Hypophysitis can present with acute symptoms associated with mass effect such as headache, photophobia, or visual field defects. Hypophysitis can cause hypopituitarism. Initiate hormone replacement as indicated. Withhold or permanently discontinue KEYTRUDA depending on severity [see Dosage and Administration (2.3)].

Hypophysitis occurred in 0.6% (17/2799) of patients receiving KEYTRUDA, including Grade 4 (<0.1%), Grade 3 (0.3%), and Grade 2 (0.2%) adverse reactions. Systemic corticosteroids were required in 94% (16/17) of patients with hypophysitis; of these, the majority remained on systemic corticosteroids. Hypophysitis led to permanent discontinuation of KEYTRUDA in 0.1% (4) of patients and withholding of KEYTRUDA in 0.3% (7) of patients. All patients who were withheld reinitiated KEYTRUDA after symptom improvement.

Thyroid Disorders

KEYTRUDA can cause immune-mediated thyroid disorders. Thyroiditis can present with or without endocrinopathy. Hypothyroidism can follow hyperthyroidism. Initiate hormone replacement for hypothyroidism or institute medical management of hyperthyroidism as clinically indicated. Withhold or permanently discontinue KEYTRUDA depending on severity [see Dosage and Administration (2.3)].

Thyroiditis occurred in 0.6% (16/2799) of patients receiving KEYTRUDA, including Grade 2 (0.3%). No patients discontinued KEYTRUDA due to thyroiditis. KEYTRUDA was withheld in <0.1% (1) of patients.

Hyperthyroidism occurred in 3.4% (96/2799) of patients receiving KEYTRUDA, including Grade 3 (0.1%) and Grade 2 (0.8%). Hyperthyroidism led to permanent discontinuation of KEYTRUDA in <0.1% (2) of patients and withholding of KEYTRUDA in 0.3% (7) of patients. All patients who were withheld reinitiated KEYTRUDA after symptom improvement.

The incidence of new or worsening hyperthyroidism was higher in 580 patients with resected NSCLC, occurring in 11% of patients receiving KEYTRUDA as a single agent as adjuvant treatment (KEYNOTE-091), including Grade 3 (0.2%) hyperthyroidism.

Hypothyroidism occurred in 8% (237/2799) of patients receiving KEYTRUDA, including Grade 3 (0.1%) and Grade 2 (6.2%). Hypothyroidism led to permanent discontinuation of KEYTRUDA in <0.1% (1) of patients and withholding of KEYTRUDA in 0.5% (14) of patients. All patients who were withheld reinitiated KEYTRUDA after symptom improvement. The majority of patients with hypothyroidism required long-term thyroid hormone replacement.

The incidence of new or worsening hypothyroidism was higher in 1185 patients with HNSCC, occurring in 16% of patients receiving KEYTRUDA as a single agent or in combination with platinum and FU, including Grade 3 (0.3%) hypothyroidism. The incidence of new or worsening hypothyroidism was higher in 389 patients with cHL (17%) receiving KEYTRUDA as a single agent, including Grade 1 (6.2%) and Grade 2 (10.8%) hypothyroidism.

The incidence of new or worsening hypothyroidism was higher in 580 patients with resected NSCLC, occurring in 22% of patients receiving KEYTRUDA as a single agent as adjuvant treatment (KEYNOTE-091), including Grade 3 (0.3%) hypothyroidism.

Type 1 Diabetes Mellitus, which can present with Diabetic Ketoacidosis

Monitor patients for hyperglycemia or other signs and symptoms of diabetes. Initiate treatment with insulin as clinically indicated. Withhold KEYTRUDA depending on severity [see Dosage and Administration (2.3)].

Type 1 diabetes mellitus occurred in 0.2% (6/2799) of patients receiving KEYTRUDA. Type 1 diabetes mellitus led to permanent discontinuation in <0.1% (1) of patients and withholding of KEYTRUDA in <0.1% (1) of patients. All patients who were withheld reinitiated KEYTRUDA after symptom improvement. All patients with Type 1 diabetes mellitus required long-term insulin therapy.

Immune-Mediated Nephritis with Renal Dysfunction

KEYTRUDA can cause immune-mediated nephritis. Immune-mediated nephritis occurred in 0.3% (9/2799) of patients receiving KEYTRUDA, including Grade 4 (<0.1%), Grade 3 (0.1%), and Grade 2 (0.1%) adverse reactions. Systemic corticosteroids were required in 89% (8/9) of patients with nephritis. Nephritis led to permanent discontinuation of KEYTRUDA in 0.1% (3) of patients and withholding of KEYTRUDA in 0.1% (3) of patients. All patients who were withheld reinitiated KEYTRUDA after symptom improvement; of these, none had recurrence of nephritis. Nephritis resolved in 56% of the 9 patients.

Immune-Mediated Dermatologic Adverse Reactions

KEYTRUDA can cause immune-mediated rash or dermatitis. Exfoliative dermatitis, including Stevens Johnson Syndrome, DRESS, and toxic epidermal necrolysis (TEN), has occurred with PD-1/PD-L1 blocking antibodies. Topical emollients and/or topical corticosteroids may be adequate to treat mild to moderate non-exfoliative rashes. Withhold or permanently discontinue KEYTRUDA depending on severity [see Dosage and Administration (2.3)].

Immune-mediated dermatologic adverse reactions occurred in 1.4% (38/2799) of patients receiving KEYTRUDA, including Grade 3 (1%) and Grade 2 (0.1%) adverse reactions. Systemic corticosteroids were required in 40% (15/38) of patients with immune-mediated dermatologic adverse reactions. Immune-mediated dermatologic adverse reactions led to permanent discontinuation of KEYTRUDA in 0.1% (2) of patients and withholding of KEYTRUDA in 0.6% (16) of patients. All patients who were withheld reinitiated KEYTRUDA after symptom improvement; of these, 6% had recurrence of immune-mediated dermatologic adverse reactions. Immune-mediated dermatologic adverse reactions resolved in 79% of the 38 patients.

Other Immune-Mediated Adverse Reactions

The following clinically significant immune-mediated adverse reactions occurred at an incidence of <1% (unless otherwise noted) in patients who received KEYTRUDA or were reported with the use of other PD-1/PD-L1 blocking antibodies. Severe or fatal cases have been reported for some of these adverse reactions.

Cardiac/Vascular: Myocarditis, pericarditis, vasculitis

Nervous System: Meningitis, encephalitis, myelitis and demyelination, myasthenic syndrome/myasthenia gravis (including exacerbation), Guillain-Barré syndrome, nerve paresis, autoimmune neuropathy

Ocular: Uveitis, iritis and other ocular inflammatory toxicities can occur. Some cases can be associated with retinal detachment. Various grades of visual impairment, including blindness, can occur. If uveitis occurs in combination with other immune-mediated adverse reactions, consider a Vogt-Koyanagi-Harada-like syndrome, as this may require treatment with systemic steroids to reduce the risk of permanent vision loss.

Gastrointestinal: Pancreatitis, to include increases in serum amylase and lipase levels, gastritis, duodenitis

Musculoskeletal and Connective Tissue: Myositis/polymyositis, rhabdomyolysis (and associated sequelae, including renal failure), arthritis (1.5%), polymyalgia rheumatica

Endocrine: Hypoparathyroidism

Hematologic/Immune: Hemolytic anemia, aplastic anemia, hemophagocytic lymphohistiocytosis, systemic inflammatory response syndrome, histiocytic necrotizing lymphadenitis (Kikuchi lymphadenitis), sarcoidosis, immune thrombocytopenic purpura, solid organ transplant rejection, other transplant (including corneal graft) rejection

5.2 Infusion-Related Reactions

KEYTRUDA can cause severe or life-threatening infusion-related reactions, including hypersensitivity and anaphylaxis, which have been reported in 0.2% of 2799 patients receiving KEYTRUDA. Monitor patients for signs and symptoms of infusion-related reactions including rigors, chills, wheezing, pruritus, flushing, rash, hypotension, hypoxemia, and fever. Interrupt or slow the rate of infusion for mild (Grade 1) or moderate (Grade 2) infusion-related reactions. For severe (Grade 3) or life-threatening (Grade 4) infusion-related reactions, stop infusion and permanently discontinue KEYTRUDA [see Dosage and Administration (2.3)].

5.3 Complications of Allogeneic HSCT

Fatal and other serious complications can occur in patients who receive allogeneic hematopoietic stem cell transplantation (HSCT) before or after being treated with a PD-1/PD-L1 blocking antibody. Transplant-related complications include hyperacute graft-versus-host-disease (GVHD), acute GVHD, chronic GVHD, hepatic veno-occlusive disease (VOD) after reduced intensity conditioning, and steroid-requiring febrile syndrome (without an identified infectious cause). These complications may occur despite intervening therapy between PD-1/PD-L1 blockade and allogeneic HSCT.

Follow patients closely for evidence of transplant-related complications and intervene promptly. Consider the benefit versus risks of treatment with a PD-1/PD-L1 blocking antibody prior to or after an allogeneic HSCT.

5.4 Increased Mortality in Patients with Multiple Myeloma when KEYTRUDA is Added to a Thalidomide Analogue and Dexamethasone

In two randomized trials in patients with multiple myeloma, the addition of KEYTRUDA to a thalidomide analogue plus dexamethasone, a use for which no PD-1 or PD-L1 blocking antibody is indicated, resulted in increased mortality. Treatment of patients with multiple myeloma with a PD-1 or PD-L1 blocking antibody in combination with a thalidomide analogue plus dexamethasone is not recommended outside of controlled trials.

5.5 Embryo-Fetal Toxicity

Based on its mechanism of action, KEYTRUDA can cause fetal harm when administered to a pregnant woman. Animal models link the PD-1/PD-L1 signaling pathway with maintenance of pregnancy through induction of maternal immune tolerance to fetal tissue. Advise women of the potential risk to a fetus. Advise females of reproductive potential to use effective contraception during treatment with KEYTRUDA and for 4 months after the last dose [see Use in Specific Populations (8.1, 8.3)].

6 ADVERSE REACTIONS

The following clinically significant adverse reactions are described elsewhere in the labeling.

- Severe and fatal immune-mediated adverse reactions [see Warnings and Precautions (5.1)].
- Infusion-related reactions [see Warnings and Precautions (5.2)].

6.1 Clinical Trials Experience

Because clinical trials are conducted under widely varying conditions, adverse reaction rates observed in the clinical trials of a drug cannot be directly compared to rates in the clinical trials of another drug and may not reflect the rates observed in practice.

The data described in the WARNINGS AND PRECAUTIONS reflect exposure to KEYTRUDA as a single agent in 2799 patients in three randomized, open-label, active-controlled trials (KEYNOTE-002, KEYNOTE-006, and KEYNOTE-010), which enrolled 912 patients with melanoma and 682 patients with NSCLC, and one single-arm trial (KEYNOTE-001), which enrolled 655 patients with melanoma and 550 patients with NSCLC. In addition to the 2799 patients, certain subsections in the WARNINGS AND PRECAUTIONS describe adverse reactions observed with exposure to KEYTRUDA as a single agent in a randomized, placebo-controlled trial (KEYNOTE-091), which enrolled 580 patients with resected NSCLC, a non-randomized, open-label, multi-cohort trial (KEYNOTE-012), a non-randomized, open-label, single-cohort trial (KEYNOTE-055), and two randomized, open-label, active-controlled trials (KEYNOTE-040 and KEYNOTE-048 single agent arms), which enrolled 909 patients with HNSCC; in two non-randomized, open-label trials (KEYNOTE-013 and KEYNOTE-087) and one randomized, open-label, active-controlled trial (KEYNOTE-204), which enrolled 389 patients with cHL; in a randomized, open-label, active-controlled trial (KEYNOTE-048 combination arm), which enrolled 276 patients with HNSCC; in combination with axitinib in a randomized, active-controlled trial (KEYNOTE-426), which enrolled 429 patients with RCC; and in post-marketing use. Across all trials, KEYTRUDA was administered at doses of 2 mg/kg intravenously every 3 weeks, 10 mg/kg intravenously every 2 weeks, 10 mg/kg intravenously every 3 weeks, or 200 mg intravenously every 3 weeks. Among the 2799 patients, 41% were exposed for 6 months or more and 21% were exposed for 12 months or more.

Melanoma

Ipilimumab-Naive Melanoma

The safety of KEYTRUDA for the treatment of patients with unresectable or metastatic melanoma who had not received prior ipilimumab and who had received no more than one prior systemic therapy was investigated in KEYNOTE-006. KEYNOTE-006 was a multicenter, open-label, active-controlled trial where patients were randomized (1:1:1) and received KEYTRUDA 10 mg/kg every 2 weeks (n=278) or KEYTRUDA 10 mg/kg every 3 weeks (n=277) until disease progression or unacceptable toxicity or ipilimumab 3 mg/kg every 3 weeks for 4 doses unless discontinued earlier for disease progression or unacceptable toxicity (n=256) [see Clinical Studies (14.1)]. Patients with autoimmune disease, a medical condition that required systemic corticosteroids or other immunosuppressive medication; a history of interstitial lung disease; or active infection requiring therapy, including HIV or hepatitis B or C, were ineligible.

The median duration of exposure was 5.6 months (range: 1 day to 11.0 months) for KEYTRUDA and similar in both treatment arms. Fifty-one and 46% of patients received KEYTRUDA 10 mg/kg every 2 or 3 weeks, respectively, for ≥6 months. No patients in either arm received treatment for more than one year.

The study population characteristics were: median age of 62 years (range: 18 to 89); 60% male; 98% White; 32% had an elevated lactate dehydrogenase (LDH) value at baseline; 65% had M1c stage disease; 9% with history of brain metastasis; and approximately 36% had been previously treated with systemic therapy which included a BRAF inhibitor (15%), chemotherapy (13%), and immunotherapy (6%).

In KEYNOTE-006, the adverse reaction profile was similar for the every 2 week and every 3 week schedule, therefore summary safety results are provided in a pooled analysis (n=555) of both KEYTRUDA arms. Adverse reactions leading to permanent discontinuation of KEYTRUDA occurred in 9% of patients. Adverse reactions leading to discontinuation of KEYTRUDA in more than one patient were colitis (1.4%), autoimmune hepatitis (0.7%), allergic reaction (0.4%), polyneuropathy (0.4%), and cardiac failure (0.4%). Adverse reactions leading to interruption of KEYTRUDA occurred in 21% of patients; the most common (≥1%) was diarrhea (2.5%). Tables 4 and 5 summarize selected adverse reactions and laboratory abnormalities, respectively, in patients on KEYTRUDA in KEYNOTE-006.

Table 4: Selected [Adverse reactions occurring at same or higher incidence than in the ipilimumab arm] Adverse Reactions Occurring in ≥10% of Patients Receiving KEYTRUDA in KEYNOTE-006
Adverse Reaction | KEYTRUDA 10 mg/kg every 2 or 3 weeks |  | Ipilimumab
Adverse Reaction | n=555 |  | n=256
 | All Grades [Graded per NCI CTCAE v4.0] (%) | Grades 3-4 (%) | All Grades (%) | Grades 3-4 (%)
General
Fatigue | 28 | 0.9 | 28 | 3.1
Skin and Subcutaneous Tissue
Rash [Includes rash, rash erythematous, rash follicular, rash generalized, rash macular, rash maculo-papular, rash papular, rash pruritic, and exfoliative rash.] | 24 | 0.2 | 23 | 1.2
Vitiligo [Includes skin hypopigmentation] | 13 | 0 | 2 | 0
Musculoskeletal and Connective Tissue
Arthralgia | 18 | 0.4 | 10 | 1.2
Back pain | 12 | 0.9 | 7 | 0.8
Respiratory, Thoracic and Mediastinal
Cough | 17 | 0 | 7 | 0.4
Dyspnea | 11 | 0.9 | 7 | 0.8
Metabolism and Nutrition
Decreased appetite | 16 | 0.5 | 14 | 0.8
Nervous System
Headache | 14 | 0.2 | 14 | 0.8

Other clinically important adverse reactions occurring in ≥10% of patients receiving KEYTRUDA were diarrhea (26%), nausea (21%), and pruritus (17%).

Table 5: Selected [Laboratory abnormalities occurring at same or higher incidence than in ipilimumab arm] Laboratory Abnormalities Worsened from Baseline Occurring in ≥20% of Melanoma Patients Receiving KEYTRUDA in KEYNOTE-006
Laboratory Test [Each test incidence is based on the number of patients who had both baseline and at least one on-study laboratory measurement available: KEYTRUDA (520 to 546 patients) and ipilimumab (237 to 247 patients); hypertriglyceridemia: KEYTRUDA n=429 and ipilimumab n=183; hypercholesterolemia: KEYTRUDA n=484 and ipilimumab n=205.] | KEYTRUDA 10 mg/kg every 2 or 3 weeks |  | Ipilimumab
 | All Grades [Graded per NCI CTCAE v4.0] % | Grades 3-4 % | All Grades % | Grades 3-4 %
Chemistry
Hyperglycemia | 45 | 4.2 | 45 | 3.8
Hypertriglyceridemia | 43 | 2.6 | 31 | 1.1
Hyponatremia | 28 | 4.6 | 26 | 7
Increased AST | 27 | 2.6 | 25 | 2.5
Hypercholesterolemia | 20 | 1.2 | 13 | 0
Hematology
Anemia | 35 | 3.8 | 33 | 4.0
Lymphopenia | 33 | 7 | 25 | 6

Other laboratory abnormalities occurring in ≥20% of patients receiving KEYTRUDA were increased hypoalbuminemia (27% all Grades; 2.4% Grades 3-4), increased ALT (23% all Grades; 3.1% Grades 3-4), and increased alkaline phosphatase (21% all Grades, 2% Grades 3-4).

Ipilimumab-Refractory Melanoma

The safety of KEYTRUDA in patients with unresectable or metastatic melanoma with disease progression following ipilimumab and, if BRAF V600 mutation positive, a BRAF inhibitor, was investigated in KEYNOTE-002. KEYNOTE-002 was a multicenter, partially blinded (KEYTRUDA dose), randomized (1:1:1), active-controlled trial in which 528 patients received KEYTRUDA 2 mg/kg (n=178) or 10 mg/kg (n=179) every 3 weeks or investigator's choice of chemotherapy (n=171), consisting of dacarbazine (26%), temozolomide (25%), paclitaxel and carboplatin (25%), paclitaxel (16%), or carboplatin (8%) [see Clinical Studies (14.1)]. Patients with autoimmune disease, severe immune-related toxicity related to ipilimumab, defined as any Grade 4 toxicity or Grade 3 toxicity requiring corticosteroid treatment (greater than 10 mg/day prednisone or equivalent dose) for greater than 12 weeks; medical conditions that required systemic corticosteroids or other immunosuppressive medication; a history of interstitial lung disease; or an active infection requiring therapy, including HIV or hepatitis B or C, were ineligible.

The median duration of exposure to KEYTRUDA 2 mg/kg every 3 weeks was 3.7 months (range: 1 day to 16.6 months) and to KEYTRUDA 10 mg/kg every 3 weeks was 4.8 months (range: 1 day to 16.8 months). In the KEYTRUDA 2 mg/kg arm, 36% of patients were exposed to KEYTRUDA for ≥6 months and 4% were exposed for ≥12 months. In the KEYTRUDA 10 mg/kg arm, 41% of patients were exposed to KEYTRUDA for ≥6 months and 6% of patients were exposed to KEYTRUDA for ≥12 months.

The study population characteristics were: median age of 62 years (range: 15 to 89); 61% male; 98% White; 41% had an elevated LDH value at baseline; 83% had M1c stage disease; 73% received two or more prior therapies for advanced or metastatic disease (100% received ipilimumab and 25% a BRAF inhibitor); and 15% with history of brain metastasis.

In KEYNOTE-002, the adverse reaction profile was similar for the 2 mg/kg dose and 10 mg/kg dose, therefore summary safety results are provided in a pooled analysis (n=357) of both KEYTRUDA arms. Adverse reactions resulting in permanent discontinuation occurred in 12% of patients receiving KEYTRUDA; the most common (≥1%) were general physical health deterioration (1%), asthenia (1%), dyspnea (1%), pneumonitis (1%), and generalized edema (1%). Adverse reactions leading to interruption of KEYTRUDA occurred in 14% of patients; the most common (≥1%) were dyspnea (1%), diarrhea (1%), and maculo-papular rash (1%). Tables 6 and 7 summarize adverse reactions and laboratory abnormalities, respectively, in patients on KEYTRUDA in KEYNOTE-002.

Table 6: Selected [Adverse reactions occurring at same or higher incidence than in chemotherapy arm] Adverse Reactions Occurring in ≥10% of Patients Receiving KEYTRUDA in KEYNOTE-002
Adverse Reaction | KEYTRUDA 2 mg/kg or 10 mg/kg every 3 weeks |  | Chemotherapy [Chemotherapy: dacarbazine, temozolomide, carboplatin plus paclitaxel, paclitaxel, or carboplatin]
Adverse Reaction | n=357 |  | n=171
 | All Grades [Graded per NCI CTCAE v4.0] (%) | Grades 3-4 (%) | All Grades (%) | Grades 3-4 (%)
Skin and Subcutaneous Tissue
Pruritus | 28 | 0 | 8 | 0
Rash [Includes rash, rash erythematous, rash generalized, rash macular, rash maculo-papular, rash papular, and rash pruritic] | 24 | 0.6 | 8 | 0
Gastrointestinal
Constipation | 22 | 0.3 | 20 | 2.3
Diarrhea | 20 | 0.8 | 20 | 2.3
Abdominal pain | 13 | 1.7 | 8 | 1.2
Respiratory, Thoracic and Mediastinal
Cough | 18 | 0 | 16 | 0
General
Pyrexia | 14 | 0.3 | 9 | 0.6
Asthenia | 10 | 2.0 | 9 | 1.8
Musculoskeletal and Connective Tissue
Arthralgia | 14 | 0.6 | 10 | 1.2

Other clinically important adverse reactions occurring in patients receiving KEYTRUDA were fatigue (43%), nausea (22%), decreased appetite (20%), vomiting (13%), and peripheral neuropathy (1.7%).

Table 7: Selected [Laboratory abnormalities occurring at same or higher incidence than in chemotherapy arm.] Laboratory Abnormalities Worsened from Baseline Occurring in ≥20% of Melanoma Patients Receiving KEYTRUDA in KEYNOTE-002
Laboratory Test [Each test incidence is based on the number of patients who had both baseline and at least one on-study laboratory measurement available: KEYTRUDA (range: 320 to 325 patients) and chemotherapy (range: 154 to 161 patients); hypertriglyceridemia: KEYTRUDA n=247 and chemotherapy n=116; decreased bicarbonate: KEYTRUDA n=263 and chemotherapy n=123.] | KEYTRUDA 2 mg/kg or 10 mg/kg every 3 weeks |  | Chemotherapy
 | All Grades [Graded per NCI CTCAE v4.0] % | Grades 3-4 % | All Grades % | Grades 3-4 %
Chemistry
Hyperglycemia | 49 | 6 | 44 | 6
Hypoalbuminemia | 37 | 1.9 | 33 | 0.6
Hyponatremia | 37 | 7 | 24 | 3.8
Hypertriglyceridemia | 33 | 0 | 32 | 0.9
Increased alkaline phosphatase | 26 | 3.1 | 18 | 1.9
Increased AST | 24 | 2.2 | 16 | 0.6
Decreased bicarbonate | 22 | 0.4 | 13 | 0
Hypocalcemia | 21 | 0.3 | 18 | 1.9
Increased ALT | 21 | 1.8 | 16 | 0.6

Other laboratory abnormalities occurring in ≥20% of patients receiving KEYTRUDA were anemia (44% all Grades; 10% Grades 3-4) and lymphopenia (40% all Grades; 9% Grades 3-4).

Adjuvant Treatment of Resected Stage IIB or IIC Melanoma

Among the 969 patients with Stage IIB or IIC melanoma enrolled in KEYNOTE-716 [see Clinical Studies (14.1)] treated with KEYTRUDA, the median duration of exposure to KEYTRUDA was 9.9 months (range: 0 to 15.4 months). Patients with autoimmune disease or a medical condition that required immunosuppression or mucosal or ocular melanoma were ineligible. Adverse reactions occurring in patients with Stage IIB or IIC melanoma were similar to those occurring in 1011 patients with Stage III melanoma from KEYNOTE-054 or the 2799 patients with melanoma or NSCLC treated with KEYTRUDA as a single agent.

Adjuvant Treatment of Stage III Resected Melanoma

The safety of KEYTRUDA as a single agent was investigated in KEYNOTE-054, a randomized (1:1) double-blind trial in which 1019 patients with completely resected Stage IIIA (>1 mm lymph node metastasis), IIIB or IIIC melanoma received 200 mg of KEYTRUDA by intravenous infusion every 3 weeks (n=509) or placebo (n=502) for up to one year [see Clinical Studies (14.1)]. Patients with active autoimmune disease or a medical condition that required immunosuppression or mucosal or ocular melanoma were ineligible. Seventy-six percent of patients received KEYTRUDA for 6 months or longer.

The study population characteristics were: median age of 54 years (range: 19 to 88), 25% age 65 or older; 62% male; and 94% ECOG PS of 0 and 6% ECOG PS of 1. Sixteen percent had Stage IIIA, 46% had Stage IIIB, 18% had Stage IIIC (1-3 positive lymph nodes), and 20% had Stage IIIC (≥4 positive lymph nodes).

Two patients treated with KEYTRUDA died from causes other than disease progression; causes of death were drug reaction with eosinophilia and systemic symptoms and autoimmune myositis with respiratory failure. Serious adverse reactions occurred in 25% of patients receiving KEYTRUDA. Adverse reactions leading to permanent discontinuation occurred in 14% of patients receiving KEYTRUDA; the most common (≥1%) were pneumonitis (1.4%), colitis (1.2%), and diarrhea (1%). Adverse reactions leading to interruption of KEYTRUDA occurred in 19% of patients; the most common (≥1%) were diarrhea (2.4%), pneumonitis (2%), increased ALT (1.4%), arthralgia (1.4%), increased AST (1.4%), dyspnea (1%), and fatigue (1%). Tables 8 and 9 summarize adverse reactions and laboratory abnormalities, respectively, in patients on KEYTRUDA in KEYNOTE-054.

Table 8: Selected [Adverse reactions occurring at same or higher incidence than in placebo arm] Adverse Reactions Occurring in ≥10% of Patients Receiving KEYTRUDA in KEYNOTE-054
Adverse Reaction | KEYTRUDA 200 mg every 3 weeks n=509 |  | Placebo n=502
Adverse Reaction | All Grades [Graded per NCI CTCAE v4.03] (%) | Grades 3-4 (%) | All Grades (%) | Grades 3-4 (%)
Gastrointestinal
Diarrhea | 28 | 1.2 | 26 | 1.2
Nausea | 17 | 0.2 | 15 | 0
Skin and Subcutaneous Tissue
Pruritus | 19 | 0 | 12 | 0
Rash | 13 | 0.2 | 9 | 0
Musculoskeletal and Connective Tissue
Arthralgia | 16 | 1.2 | 14 | 0
Endocrine
Hypothyroidism | 15 | 0 | 2.8 | 0
Hyperthyroidism | 10 | 0.2 | 1.2 | 0
Respiratory, Thoracic and Mediastinal
Cough | 14 | 0 | 11 | 0
General
Asthenia | 11 | 0.2 | 8 | 0
Influenza like illness | 11 | 0 | 8 | 0
Investigations
Weight loss | 11 | 0 | 8 | 0

Table 9: Selected [Laboratory abnormalities occurring at same or higher incidence than placebo.] Laboratory Abnormalities Worsened from Baseline Occurring in ≥20% of Melanoma Patients Receiving KEYTRUDA in KEYNOTE-054
Laboratory Test [Each test incidence is based on the number of patients who had both baseline and at least one on-study laboratory measurement available: KEYTRUDA (range: 502 to 505 patients) and placebo (range: 491 to 497 patients).] | KEYTRUDA 200 mg every 3 weeks |  | Placebo
Laboratory Test [Each test incidence is based on the number of patients who had both baseline and at least one on-study laboratory measurement available: KEYTRUDA (range: 502 to 505 patients) and placebo (range: 491 to 497 patients).] | All Grades [Graded per NCI CTCAE v4.03] % | Grades 3-4 % | All Grades % | Grades 3-4 %
Chemistry
Increased ALT | 25 | 2.4 | 15 | 0.2
Increased AST | 22 | 1.8 | 14 | 0.4
Hematology
Lymphopenia | 22 | 1 | 15 | 1.2

NSCLC

First-line treatment of metastatic nonsquamous NSCLC with pemetrexed and platinum chemotherapy

The safety of KEYTRUDA in combination with pemetrexed and investigator's choice of platinum (either carboplatin or cisplatin) was investigated in KEYNOTE-189, a multicenter, double-blind, randomized (2:1), active-controlled trial in patients with previously untreated, metastatic nonsquamous NSCLC with no EGFR or ALK genomic tumor aberrations [see Clinical Studies (14.2)]. A total of 607 patients received KEYTRUDA 200 mg, pemetrexed and platinum every 3 weeks for 4 cycles followed by KEYTRUDA and pemetrexed (n=405) or placebo, pemetrexed, and platinum every 3 weeks for 4 cycles followed by placebo and pemetrexed (n=202). Patients with autoimmune disease that required systemic therapy within 2 years of treatment; a medical condition that required immunosuppression; or who had received more than 30 Gy of thoracic radiation within the prior 26 weeks were ineligible.

The median duration of exposure to KEYTRUDA 200 mg every 3 weeks was 7.2 months (range: 1 day to 20.1 months). Sixty percent of patients in the KEYTRUDA arm were exposed to KEYTRUDA for ≥6 months. Seventy-two percent of patients received carboplatin.

The study population characteristics were: median age of 64 years (range: 34 to 84), 49% age 65 or older; 59% male; 94% White and 3% Asian; and 18% with history of brain metastases at baseline.

KEYTRUDA was discontinued for adverse reactions in 20% of patients. The most common adverse reactions resulting in permanent discontinuation of KEYTRUDA were pneumonitis (3%) and acute kidney injury (2%). Adverse reactions leading to the interruption of KEYTRUDA occurred in 53% of patients; the most common adverse reactions or laboratory abnormalities leading to interruption of KEYTRUDA (≥2%) were neutropenia (13%), asthenia/fatigue (7%), anemia (7%), thrombocytopenia (5%), diarrhea (4%), pneumonia (4%), increased blood creatinine (3%), dyspnea (2%), febrile neutropenia (2%), upper respiratory tract infection (2%), increased ALT (2%), and pyrexia (2%). Tables 10 and 11 summarize adverse reactions and laboratory abnormalities, respectively, in patients on KEYTRUDA in KEYNOTE-189.

Table 10: Adverse Reactions Occurring in ≥20% of Patients in KEYNOTE-189
Adverse Reaction | KEYTRUDA 200 mg every 3 weeks Pemetrexed Platinum Chemotherapy n=405 |  | Placebo Pemetrexed Platinum Chemotherapy n=202
 | All Grades [Graded per NCI CTCAE v4.03] (%) | Grades 3-4 (%) | All Grades (%) | Grades 3-4 (%)
Gastrointestinal
Nausea | 56 | 3.5 | 52 | 3.5
Constipation | 35 | 1.0 | 32 | 0.5
Diarrhea | 31 | 5 | 21 | 3.0
Vomiting | 24 | 3.7 | 23 | 3.0
General
Fatigue [Includes asthenia and fatigue] | 56 | 12 | 58 | 6
Pyrexia | 20 | 0.2 | 15 | 0
Metabolism and Nutrition
Decreased appetite | 28 | 1.5 | 30 | 0.5
Skin and Subcutaneous Tissue
Rash [Includes genital rash, rash, rash generalized, rash macular, rash maculo-papular, rash papular, rash pruritic, and rash pustular.] | 25 | 2.0 | 17 | 2.5
Respiratory, Thoracic and Mediastinal
Cough | 21 | 0 | 28 | 0
Dyspnea | 21 | 3.7 | 26 | 5

Table 11: Laboratory Abnormalities Worsened from Baseline Occurring in ≥20% of Patients in KEYNOTE-189
Laboratory Test [Each test incidence is based on the number of patients who had both baseline and at least one on-study laboratory measurement available: KEYTRUDA/pemetrexed/platinum chemotherapy (range: 381 to 401 patients) and placebo/pemetrexed/platinum chemotherapy (range: 184 to 197 patients).] | KEYTRUDA 200 mg every 3 weeks Pemetrexed Platinum Chemotherapy |  | Placebo Pemetrexed Platinum Chemotherapy
 | All Grades [Graded per NCI CTCAE v4.03] % | Grades 3-4 % | All Grades % | Grades 3-4 %
Hematology
Anemia | 85 | 17 | 81 | 18
Lymphopenia | 65 | 22 | 64 | 25
Neutropenia | 50 | 21 | 41 | 19
Thrombocytopenia | 30 | 12 | 29 | 8
Chemistry
Hyperglycemia | 63 | 9 | 60 | 7
Increased ALT | 47 | 3.8 | 42 | 2.6
Increased AST | 47 | 2.8 | 40 | 1.0
Hypoalbuminemia | 39 | 2.8 | 39 | 1.1
Increased creatinine | 37 | 4.2 | 25 | 1.0
Hyponatremia | 32 | 7 | 23 | 6
Hypophosphatemia | 30 | 10 | 28 | 14
Increased alkaline phosphatase | 26 | 1.8 | 29 | 2.1
Hypocalcemia | 24 | 2.8 | 17 | 0.5
Hyperkalemia | 24 | 2.8 | 19 | 3.1
Hypokalemia | 21 | 5 | 20 | 5

First-line treatment of metastatic squamous NSCLC with carboplatin and either paclitaxel or paclitaxel protein-bound chemotherapy

The safety of KEYTRUDA in combination with carboplatin and investigator's choice of either paclitaxel or paclitaxel protein-bound was investigated in KEYNOTE-407, a multicenter, double-blind, randomized (1:1), placebo-controlled trial in 558 patients with previously untreated, metastatic squamous NSCLC [see Clinical Studies (14.2)]. Safety data are available for the first 203 patients who received KEYTRUDA and chemotherapy (n=101) or placebo and chemotherapy (n=102). Patients with autoimmune disease that required systemic therapy within 2 years of treatment; a medical condition that required immunosuppression; or who had received more than 30 Gy of thoracic radiation within the prior 26 weeks were ineligible.

The median duration of exposure to KEYTRUDA was 7 months (range: 1 day to 12 months). Sixty-one percent of patients in the KEYTRUDA arm were exposed to KEYTRUDA for ≥6 months. A total of 139 of 203 patients (68%) received paclitaxel and 64 patients (32%) received paclitaxel protein-bound in combination with carboplatin.

The study population characteristics were: median age of 65 years (range: 40 to 83), 52% age 65 or older; 78% male; 83% White; and 9% with history of brain metastases.

KEYTRUDA was discontinued for adverse reactions in 15% of patients, with no single type of adverse reaction accounting for the majority. Adverse reactions leading to interruption of KEYTRUDA occurred in 43% of patients; the most common (≥2%) were thrombocytopenia (20%), neutropenia (11%), anemia (6%), asthenia (2%), and diarrhea (2%). The most frequent (≥2%) serious adverse reactions were febrile neutropenia (6%), pneumonia (6%), and urinary tract infection (3%).

The adverse reactions observed in KEYNOTE-407 were similar to those observed in KEYNOTE-189 with the exception that increased incidences of alopecia (47% vs. 36%) and peripheral neuropathy (31% vs. 25%) were observed in the KEYTRUDA and chemotherapy arm compared to the placebo and chemotherapy arm in KEYNOTE-407.

Previously Untreated NSCLC

The safety of KEYTRUDA was investigated in KEYNOTE-042, a multicenter, open-label, randomized (1:1), active-controlled trial in 1251 patients with PD-L1 expressing, previously untreated Stage III NSCLC who were not candidates for surgical resection or definitive chemoradiation or metastatic NSCLC [see Clinical Studies (14.2)]. Patients received KEYTRUDA 200 mg every 3 weeks (n=636) or investigator's choice of chemotherapy (n=615), consisting of pemetrexed and carboplatin followed by optional pemetrexed (n=312) or paclitaxel and carboplatin followed by optional pemetrexed (n=303) every 3 weeks. Patients with EGFR or ALK genomic tumor aberrations; autoimmune disease that required systemic therapy within 2 years of treatment; a medical condition that required immunosuppression; or who had received more than 30 Gy of thoracic radiation within the prior 26 weeks were ineligible.

The median duration of exposure to KEYTRUDA was 5.6 months (range: 1 day to 27.3 months). Forty-eight percent of patients in the KEYTRUDA arm were exposed to KEYTRUDA 200 mg for ≥6 months.

The study population characteristics were: median age of 63 years (range: 25 to 90), 45% age 65 or older; 71% male; and 64% White, 30% Asian, and 2% Black. Nineteen percent were Hispanic or Latino. Eighty-seven percent had metastatic disease (Stage IV), 13% had Stage III disease (2% Stage IIIA and 11% Stage IIIB), and 5% had treated brain metastases at baseline.

KEYTRUDA was discontinued for adverse reactions in 19% of patients. The most common adverse reactions resulting in permanent discontinuation of KEYTRUDA were pneumonitis (3.0%), death due to unknown cause (1.6%), and pneumonia (1.4%). Adverse reactions leading to interruption of KEYTRUDA occurred in 33% of patients; the most common adverse reactions or laboratory abnormalities leading to interruption of KEYTRUDA (≥2%) were pneumonitis (3.1%), pneumonia (3.0%), hypothyroidism (2.2%), and increased ALT (2.0%). The most frequent (≥2%) serious adverse reactions were pneumonia (7%), pneumonitis (3.9%), pulmonary embolism (2.4%), and pleural effusion (2.2%).

Tables 12 and 13 summarize the adverse reactions and laboratory abnormalities, respectively, in patients treated with KEYTRUDA in KEYNOTE-042.

Table 12: Adverse Reactions Occurring in ≥10% of Patients in KEYNOTE-042
Adverse Reaction | KEYTRUDA 200 mg every 3 weeks n=636 |  | Chemotherapy n=615
Adverse Reaction | All Grades [Graded per NCI CTCAE v4.03] (%) | Grades 3-5 (%) | All Grades (%) | Grades 3-5 (%)
General
Fatigue [Includes fatigue and asthenia] | 25 | 3.1 | 33 | 3.9
Pyrexia | 10 | 0.3 | 8 | 0
Metabolism and Nutrition
Decreased appetite | 17 | 1.7 | 21 | 1.5
Respiratory, Thoracic and Mediastinal
Dyspnea | 17 | 2.0 | 11 | 0.8
Cough | 16 | 0.2 | 11 | 0.3
Skin and Subcutaneous Tissue
Rash [Includes rash, rash generalized, rash macular, rash maculo-papular, rash papular, rash pruritic, and rash pustular.] | 15 | 1.3 | 8 | 0.2
Gastrointestinal
Constipation | 12 | 0 | 21 | 0.2
Diarrhea | 12 | 0.8 | 12 | 0.5
Nausea | 12 | 0.5 | 32 | 1.1
Endocrine
Hypothyroidism | 12 | 0.2 | 1.5 | 0
Infections
Pneumonia | 12 | 7 | 9 | 6
Investigations
Weight loss | 10 | 0.9 | 7 | 0.2

Table 13: Laboratory Abnormalities Worsened from Baseline in ≥20% of Patients in KEYNOTE-042
Laboratory Test [Each test incidence is based on the number of patients who had both baseline and at least one on-study laboratory measurement available: KEYTRUDA (range: 598 to 610 patients) and chemotherapy (range: 585 to 598 patients); increased prothrombin INR: KEYTRUDA n=203 and chemotherapy n=173.] | KEYTRUDA 200 mg every 3 weeks |  | Chemotherapy
Laboratory Test [Each test incidence is based on the number of patients who had both baseline and at least one on-study laboratory measurement available: KEYTRUDA (range: 598 to 610 patients) and chemotherapy (range: 585 to 598 patients); increased prothrombin INR: KEYTRUDA n=203 and chemotherapy n=173.] | All Grades [Graded per NCI CTCAE v4.03] % | Grades 3-4 % | All Grades % | Grades 3-4 %
Chemistry
Hyperglycemia | 52 | 4.7 | 51 | 5
Increased ALT | 33 | 4.8 | 34 | 2.9
Hypoalbuminemia | 33 | 2.2 | 29 | 1.0
Increased AST | 31 | 3.6 | 32 | 1.7
Hyponatremia | 31 | 9 | 32 | 8
Increased alkaline phosphatase | 29 | 2.3 | 29 | 0.3
Hypocalcemia | 25 | 2.5 | 19 | 0.7
Hyperkalemia | 23 | 3.0 | 20 | 2.2
Increased prothrombin INR | 21 | 2.0 | 15 | 2.9
Hypophosphatemia | 20 | 4.7 | 17 | 4.3
Hematology
Anemia | 43 | 4.4 | 79 | 19
Lymphopenia | 30 | 7 | 42 | 13

Previously Treated NSCLC

The safety of KEYTRUDA was investigated in KEYNOTE-010, a multicenter, open-label, randomized (1:1:1), active-controlled trial, in patients with advanced NSCLC who had documented disease progression following treatment with platinum-based chemotherapy and, if positive for EGFR or ALK genetic aberrations, appropriate therapy for these aberrations [see Clinical Studies (14.2)]. A total of 991 patients received KEYTRUDA 2 mg/kg (n=339) or 10 mg/kg (n=343) every 3 weeks or docetaxel (n=309) at 75 mg/m^2 every 3 weeks. Patients with autoimmune disease, medical conditions that required systemic corticosteroids or other immunosuppressive medication, or who had received more than 30 Gy of thoracic radiation within the prior 26 weeks were ineligible.

The median duration of exposure to KEYTRUDA 2 mg/kg every 3 weeks was 3.5 months (range: 1 day to 22.4 months) and to KEYTRUDA 10 mg/kg every 3 weeks was 3.5 months (range 1 day to 20.8 months). The data described below reflect exposure to KEYTRUDA 2 mg/kg in 31% of patients exposed to KEYTRUDA for ≥6 months. In the KEYTRUDA 10 mg/kg arm, 34% of patients were exposed to KEYTRUDA for ≥6 months.

The study population characteristics were: median age of 63 years (range: 20 to 88), 42% age 65 or older; 61% male; 72% White and 21% Asian; and 8% with advanced localized disease, 91% with metastatic disease, and 15% with history of brain metastases. Twenty-nine percent received two or more prior systemic treatments for advanced or metastatic disease.

In KEYNOTE-010, the adverse reaction profile was similar for the 2 mg/kg and 10 mg/kg dose, therefore summary safety results are provided in a pooled analysis (n=682). Treatment was discontinued for adverse reactions in 8% of patients receiving KEYTRUDA. The most common adverse events resulting in permanent discontinuation of KEYTRUDA was pneumonitis (1.8%). Adverse reactions leading to interruption of KEYTRUDA occurred in 23% of patients; the most common (≥1%) were diarrhea (1%), fatigue (1.3%), pneumonia (1%), liver enzyme elevation (1.2%), decreased appetite (1.3%), and pneumonitis (1%). Tables 14 and 15 summarize adverse reactions and laboratory abnormalities, respectively, in patients on KEYTRUDA in KEYNOTE-010.

Table 14: Selected [Adverse reactions occurring at same or higher incidence than in docetaxel arm] Adverse Reactions Occurring in ≥10% of Patients Receiving KEYTRUDA in KEYNOTE-010
Adverse Reaction | KEYTRUDA 2 or 10 mg/kg every 3 weeks n=682 |  | Docetaxel 75 mg/m^2 every 3 weeks n=309
 | All Grades [Graded per NCI CTCAE v4.0] (%) | Grades 3-4 (%) | All Grades (%) | Grades 3-4 (%)
Metabolism and Nutrition
Decreased appetite | 25 | 1.5 | 23 | 2.6
Respiratory, Thoracic and Mediastinal
Dyspnea | 23 | 3.7 | 20 | 2.6
Cough | 19 | 0.6 | 14 | 0
Gastrointestinal
Nausea | 20 | 1.3 | 18 | 0.6
Constipation | 15 | 0.6 | 12 | 0.6
Vomiting | 13 | 0.9 | 10 | 0.6
Skin and Subcutaneous Tissue
Rash [Includes rash, rash erythematous, rash macular, rash maculo-papular, rash papular, and rash pruritic] | 17 | 0.4 | 8 | 0
Pruritus | 11 | 0 | 3 | 0.3
Musculoskeletal and Connective Tissue
Arthralgia | 11 | 1.0 | 9 | 0.3
Back pain | 11 | 1.5 | 8 | 0.3

Other clinically important adverse reactions occurring in patients receiving KEYTRUDA were fatigue (25%), diarrhea (14%), asthenia (11%) and pyrexia (11%).

Table 15: Selected [Laboratory abnormalities occurring at same or higher incidence than in docetaxel arm.] Laboratory Abnormalities Worsened from Baseline Occurring in ≥20% of NSCLC Patients Receiving KEYTRUDA in KEYNOTE-010
Laboratory Test [Each test incidence is based on the number of patients who had both baseline and at least one on-study laboratory measurement available: KEYTRUDA (range: 631 to 638 patients) and docetaxel (range: 271 to 277 patients).] | KEYTRUDA 2 or 10 mg/kg every 3 weeks |  | Docetaxel 75 mg/m^2 every 3 weeks
 | All Grades [Graded per NCI CTCAE v4.0] % | Grades 3-4 % | All Grades % | Grades 3-4 %
Chemistry
Hyponatremia | 32 | 8 | 27 | 2.9
Increased alkaline phosphatase | 28 | 3.0 | 16 | 0.7
Increased AST | 26 | 1.6 | 12 | 0.7
Increased ALT | 22 | 2.7 | 9 | 0.4
Hypocalcemia | 20 | 0.9 | 20 | 1.8

Other laboratory abnormalities occurring in ≥20% of patients receiving KEYTRUDA were hyperglycemia (44% all Grades; 4.1% Grades 3-4), anemia (37% all Grades; 3.8% Grades 3-4), hypertriglyceridemia (36% all Grades; 1.8% Grades 3-4), lymphopenia (32% all Grades; 9% Grades 3-4), hypoalbuminemia (34% all Grades; 1.6% Grades 3-4), and hypercholesterolemia (20% all Grades; 0.7% Grades 3-4).

Neoadjuvant and Adjuvant Treatment of Resectable NSCLC

The safety of KEYTRUDA in combination with neoadjuvant platinum-containing chemotherapy followed by surgery and continued adjuvant treatment with KEYTRUDA as a single agent after surgery was investigated in KEYNOTE-671, a multicenter, randomized (1:1), double-blind, placebo-controlled trial in patients with previously untreated and resectable Stage II, IIIA, or IIIB (N2) NSCLC by AJCC 8th edition [see Clinical Studies (14.2)]. Patients with active autoimmune disease that required systemic therapy within 2 years of treatment or a medical condition that required immunosuppression were ineligible.

The median duration of exposure to KEYTRUDA 200 mg every 3 weeks was 10.9 months (range: 1 day to 18.6 months). The study population characteristics were: median age of 64 years (range: 26 to 83), 45% age 65 or older, 7% age 75 or older; 71% male; 61% White, 31% Asian, 2% Black, 4% race not reported; 9% Hispanic or Latino.

Adverse reactions occurring in patients with resectable NSCLC receiving KEYTRUDA in combination with platinum containing chemotherapy, given as neoadjuvant treatment and continued as single agent adjuvant treatment, were generally similar to those occurring in patients in other clinical trials across tumor types receiving KEYTRUDA in combination with chemotherapy.

Neoadjuvant Phase of KEYNOTE-671

A total of 396 patients received at least 1 dose of KEYTRUDA in combination with platinum-containing chemotherapy as neoadjuvant treatment and 399 patients received at least 1 dose of placebo in combination with platinum-containing chemotherapy as neoadjuvant treatment.

Serious adverse reactions occurred in 34% of patients who received KEYTRUDA in combination with platinum-containing chemotherapy as neoadjuvant treatment; the most frequent (≥2%) serious adverse reactions were pneumonia (4.8%), venous thromboembolism (3.3%), and anemia (2%). Fatal adverse reactions occurred in 1.3% of patients, including death due to unknown cause (0.8%), sepsis (0.3%), and immune-mediated lung disease (0.3%).

Permanent discontinuation of any study drug due to an adverse reaction occurred in 18% of patients who received KEYTRUDA in combination with platinum-containing chemotherapy as neoadjuvant treatment; the most frequent (≥1%) adverse reactions that led to permanent discontinuation of any study drug were acute kidney injury (1.8%), interstitial lung disease (1.8%), anemia (1.5%), neutropenia (1.5%), and pneumonia (1.3%).

Of the 396 KEYTRUDA-treated patients and 399 placebo-treated patients who received neoadjuvant treatment, 6% (n=25) and 4.3% (n=17), respectively, did not receive surgery due to adverse reactions. The most frequent (≥1%) adverse reactions that led to cancellation of surgery in the KEYTRUDA arm was interstitial lung disease (1%).

Of the 325 KEYTRUDA-treated patients who received surgery, 3.1% (n=10) experienced delay of surgery (surgery more than 8 weeks from last neoadjuvant treatment if patient received less than 4 cycles of neoadjuvant therapy or more than 20 weeks after first dose of neoadjuvant treatment if patient received 4 cycles of neoadjuvant therapy) due to adverse reactions. Of the 317 placebo-treated patients who received surgery, 2.5% (n=8) experienced delay of surgery due to adverse reactions.

Of the 325 KEYTRUDA-treated patients who received surgery, 7% (n=22) did not receive adjuvant treatment due to adverse reactions. Of the 317 placebo-treated patients who received surgery, 3.2% (n=10) did not receive adjuvant treatment due to adverse reactions.

Adjuvant Phase of KEYNOTE-671

A total of 290 patients in the KEYTRUDA arm and 267 patients in the placebo arm received at least 1 dose of adjuvant treatment.

Of the patients who received single agent KEYTRUDA as adjuvant treatment, 14% experienced serious adverse reactions; the most frequent serious adverse reaction was pneumonia (3.4%). One fatal adverse reaction of pulmonary hemorrhage occurred. Permanent discontinuation of adjuvant KEYTRUDA due to an adverse reaction occurred in 12% of patients; the most frequent (≥1%) adverse reactions that led to permanent discontinuation of adjuvant KEYTRUDA were diarrhea (1.7%), interstitial lung disease (1.4%), AST increased (1%), and musculoskeletal pain (1%).

Adjuvant Treatment of Resected NSCLC

The safety of KEYTRUDA as a single agent was investigated in KEYNOTE-091, a multicenter, randomized (1:1), triple-blind, placebo-controlled trial in patients with completely resected Stage IB (T2a ≥4 cm), II, or IIIA NSCLC; adjuvant chemotherapy up to 4 cycles was optional [see Clinical Studies (14.2)]. A total of 1161 patients received KEYTRUDA 200 mg (n=580) or placebo (n=581) every 3 weeks. Patients were ineligible if they had active autoimmune disease, were on chronic immunosuppressive agents, or had a history of interstitial lung disease or pneumonitis.

The median duration of exposure to KEYTRUDA was 11.7 months (range: 1 day to 18.9 months). Sixty-eight percent of patients in the KEYTRUDA arm were exposed to KEYTRUDA for ≥6 months.

The adverse reactions observed in KEYNOTE-091 were generally similar to those occurring in other patients with NSCLC receiving KEYTRUDA as a single agent, with the exception of hypothyroidism (22%), hyperthyroidism (11%), and pneumonitis (7%). Two fatal adverse reactions of myocarditis occurred.

Malignant Pleural Mesothelioma (MPM)

First-line treatment of unresectable advanced or metastatic MPM with pemetrexed and platinum chemotherapy

The safety of KEYTRUDA in combination with pemetrexed and platinum chemotherapy (either carboplatin or cisplatin) was investigated in KEYNOTE-483, a multicenter, open-label, randomized (1:1), active-controlled trial in patients with previously untreated, unresectable advanced or metastatic MPM [see Clinical Studies (14.3)]. A total of 473 patients received KEYTRUDA 200 mg, pemetrexed, and platinum every 3 weeks for up to 6 cycles followed by KEYTRUDA (n=241), or pemetrexed and platinum chemotherapy every 3 weeks for up to 6 cycles (n=232). Patients with autoimmune disease that required systemic therapy within 3 years of treatment or a medical condition that required immunosuppression were ineligible.

The median duration of exposure to KEYTRUDA 200 mg every 3 weeks was 6.9 months (range: 1 day to 25.2 months). Sixty-one percent of patients in the KEYTRUDA arm were exposed to KEYTRUDA for ≥6 months.

Adverse reactions occurring in patients with MPM were generally similar to those in other patients receiving KEYTRUDA in combination with pemetrexed and platinum chemotherapy.

HNSCC

Neoadjuvant and Adjuvant Treatment of Locally Advanced HNSCC

The safety of KEYTRUDA as neoadjuvant and adjuvant treatment added to standard of care (SOC) therapy was evaluated in KEYNOTE-689, a multicenter, randomized (1:1), open-label, active-controlled trial in patients with resectable locally advanced (Stage III-IVA by AJCC 8th edition) head and neck squamous cell carcinoma (HNSCC) [see Clinical Studies (14.4)]. KEYTRUDA was administered as single-agent neoadjuvant therapy before definitive surgery, during adjuvant radiotherapy (RT) with or without concurrent cisplatin, and then as single agent adjuvant therapy. Concurrent cisplatin was added to KEYTRUDA and adjuvant RT for high-risk disease pathology. A total of 361 patients received treatment on the KEYTRUDA arm and 315 patients received treatment on the SOC therapy arm.

The median duration of exposure to KEYTRUDA in the neoadjuvant phase was 3.1 weeks (range: 1 day to 4.9 weeks). The median duration of exposure to KEYTRUDA in the adjuvant phase was 42 weeks (range: 1 day to 82 weeks).

The median age of patients who received KEYTRUDA was 60 years (range: 29 to 82), 32% age 65 or older, 6% age 75 or older; 79% male; 78% White, 14% Asian, 2.2% Black or African American, 2% Other races, 2.7% unknown race; and 15% Hispanic or Latino.

The most common adverse reactions (≥ 20%) on the KEYTRUDA arm were stomatitis (48%), radiation skin injury (40%), weight loss (36%), fatigue (33%), dysphagia (29%), constipation (27%), hypothyroidism (26%), nausea (24%), rash (22%), dry mouth (22%), diarrhea (22%), and musculoskeletal pain (22%).

Table 16 and Table 17 summarize adverse reactions and laboratory abnormalities, respectively, in patients on KEYTRUDA in KEYNOTE-689.

Table 16: Adverse Reactions in ≥20% of Patients with HNSCC Who Received KEYTRUDA in KEYNOTE-689
Adverse Reaction | KEYTRUDA Neoadjuvant then adjuvant beginning with RT with or without cisplatin n=361 |  | Standard of Care Adjuvant RT with or without cisplatin n=315
 | All Grades [Graded per NCI CTCAE v4.03] (%) | Grade 3or 4 (%) | All Grades (%) | Grade 3 or 4 (%)
Gastrointestinal
Stomatitis [Includes pharyngeal inflammation, cheilitis, oral mucosal erythema, mucosal inflammation, glossitis, mouth ulceration, tongue ulceration] | 48 | 14 | 60 | 13
Dysphagia | 29 | 12 | 32 | 11
Constipation | 27 | 0.3 | 22 | 0.3
Nausea | 24 | 1.9 | 28 | 2.9
Dry mouth | 22 | 1.4 | 26 | 1.6
Diarrhea [Includes colitis, enteritis, hemorrhagic diarrhea] | 22 | 4.2 | 11 | 0.6
Injury, poisoning and procedural complications
Radiation skin injury | 40 | 4.2 | 48 | 5.7
Investigations
Weight loss | 36 | 14 | 27 | 10
Endocrine disorders
Hypothyroidism [Includes blood thyroid stimulating hormone increased] | 26 | 0 | 6 | 0
General
Fatigue [Includes asthenia] | 33 | 2.2 | 27 | 1.6
Skin and subcutaneous tissue disorders
Rash [Includes dermatitis, skin exfoliation, dermatitis acneiform, eczema, rash macular, rash maculo-papular, erythema multiforme, dermatitis exfoliative, urticarial dermatitis, eczema asteatotic, exfoliative rash, rash pruritic, rash pustular] | 22 | 1.9 | 10 | 1.9
Musculoskeletal and connective tissue disorders
Musculoskeletal pain [Includes neck pain, arthralgia, pain in extremity, back pain, myalgia, bone pain, arthritis, non-cardiac chest pain, musculoskeletal chest pain, musculoskeletal stiffness, spinal pain] | 22 | 1.9 | 16 | 0.6

Table 17: Select Laboratory Abnormalities (≥20%) that Worsened from Baseline in Patients with HNSCC Who Received KEYTRUDA in KEYNOTE-689
Laboratory Test [Each test incidence is based on the number of patients who had both baseline and at least one on-study laboratory measurement available: KEYTRUDA + CRT/RT (range: 342 to 357 patients) and CRT/RT (range: 300 to 309 patients)] | KEYTRUDA Neoadjuvant then adjuvant beginning with radiation with or without cisplatin |  | Radiation with or without cisplatin
Laboratory Test [Each test incidence is based on the number of patients who had both baseline and at least one on-study laboratory measurement available: KEYTRUDA + CRT/RT (range: 342 to 357 patients) and CRT/RT (range: 300 to 309 patients)] | All Grades [Graded per NCI CTCAE v4.03] (%) | Grades 3-4 (%) | All Grades (%) | Grades 3-4 (%)
Hematology
Lymphopenia | 76 | 50 | 86 | 55
Anemia | 75 | 12 | 74 | 12
Neutropenia | 32 | 13 | 35 | 19
Thrombocytopenia | 22 | 1.7 | 29 | 1.9
Chemistry
Hyperglycemia | 57 | 5.7 | 47 | 2.7
Hyponatremia | 47 | 16 | 36 | 11
Increased ALT | 42 | 6.2 | 37 | 2.0
Hypoalbuminemia | 40 | 1.4 | 38 | 1.0
Increased AST | 38 | 4.8 | 23 | 2.0
Hypomagnesemia | 34 | 1.2 | 22 | 1.3
Hypokalemia | 29 | 6.8 | 20 | 7.4
Hyperkalemia | 29 | 3.4 | 24 | 2.3
Increased alkaline phosphatase | 27 | 2.5 | 19 | 0.0
Hypocalcemia | 27 | 2.6 | 26 | 3.3
Hypophosphatemia | 23 | 6.1 | 15 | 7.0
Increased creatinine | 22 | 2.0 | 27 | 2.9
Hypercalcemia | 21 | 2.0 | 14 | 1.3

Neoadjuvant Phase of KEYNOTE 689

Of the 361 patients who received at least one dose of single agent KEYTRUDA as neoadjuvant treatment, 11% of patients experienced serious adverse reactions. Serious adverse reactions that occurred in more than one patient were pneumonia (1.4%), tumor hemorrhage (0.8%), dysphagia (0.6%), immune mediated hepatitis (0.6%), cellulitis (0.6%), and dyspnea (0.6%). Fatal adverse reactions occurred in 1.1% of patients who received neoadjuvant KEYTRUDA including respiratory failure, clostridium infection, septic shock, and myocardial infarction (one patient each).

Permanent discontinuation of KEYTRUDA due to an adverse reaction occurred in 2.8% of patients who received KEYTRUDA as neoadjuvant treatment. The most frequent adverse reaction which resulted in permanent discontinuation of neoadjuvant KEYTRUDA in more than one patient was arthralgia (0.6%).

Of the 361 patients who received KEYTRUDA as neoadjuvant treatment, 11% (n=38) did not receive surgery. Surgical cancellation on the KEYTRUDA arm was due to disease progression in 4% (n=15), patient decision in 3% (n=10), adverse reactions in 1.4% (n=5), physician’s decision in 1.1% (n=4), unresectable tumor in 0.6% (n=2), loss of follow-up in 0.3% (n=1), and use of non-study anti-cancer therapy in 0.3% (n=1).

Of the 351 patients randomized to SOC, 12% (n=43) did not receive surgery. Surgical cancellation on the SOC arm was due to patient decision in 7% (n=24), physician’s decision in 2.3% (n=8), disease progression in 1.7% (n=6), and adverse reactions in 1.4% (n=5).

Of the 323 KEYTRUDA-treated patients who received surgery, 1.2% (n=4) experienced delay of surgery (defined as on-study surgery occurring ≥ 9 weeks after initiation of neoadjuvant KEYTRUDA) due to adverse reactions. Of the 307 patients randomized to SOC who received surgery on study, 0.3% (n=1) experienced delay of surgery (defined as surgery occurring ≥ 6 weeks after randomization) due to adverse reactions

Among the KEYTRUDA-treated patients who received surgery, 2.8% (n=9) did not receive adjuvant treatment due to adverse reactions. Among the SOC-treated patients who received surgery, 3.6% (n=11) did not receive adjuvant RT or chemoradiation due to adverse reactions.

Adjuvant Phase of KEYNOTE 689

A total of 275 patients in the KEYTRUDA arm and 275 patients in the SOC arm started the adjuvant phase of treatment. On the KEYTRUDA arm, 100 patients received KEYTRUDA and cisplatin with concurrent RT, 154 patients received KEYTRUDA alone with concurrent RT, 7 patients received cisplatin alone with concurrent RT, and 13 patients received RT alone. One patient received KEYTRUDA alone. On the SOC arm, 139 patients received cisplatin with concurrent RT while 136 patients received RT alone. For the KEYTRUDA arm, a total of 222 patients received single-agent KEYTRUDA following RT.

Of the 255 patients who received at least one dose of KEYTRUDA in the adjuvant phase, 38% experienced serious adverse reactions. The most frequent serious adverse reactions reported in ≥1% of KEYTRUDA-treated patients were pneumonia (2.7%), pyrexia (2.4%), stomatitis (2.4%), acute kidney injury (2.0%), pneumonitis (1.6%), COVID-19 (1.2%), death not otherwise specified (1.2%), diarrhea (1.2%), dysphagia (1.2%), gastrostomy tube site complication (1.2%), and immune-mediated hepatitis (1.2%).

Fatal adverse reactions occurred in 5% including death not otherwise specified (1.2%), acute renal failure (0.4%), hypercalcemia (0.4%), pulmonary hemorrhage (0.4%), dysphagia/malnutrition (0.4%), mesenteric thrombosis (0.4%), sepsis (0.4%), pneumonia (0.4%), COVID-19 (0.4%), respiratory failure (0.4%), cardiovascular disorder (0.4%) and gastrointestinal hemorrhage (0.4%).

Permanent discontinuation of adjuvant KEYTRUDA due to an adverse reaction occurred in 17% of patients. The most frequent (≥1%) adverse reactions that led to permanent discontinuation of adjuvant KEYTRUDA were pneumonitis, colitis, immune-mediated hepatitis and death not otherwise specified.

Of the 275 patients who received SOC in the adjuvant phase, 23% experienced serious adverse reactions.

The most frequent serious adverse reactions reported in >1% of SOC-treated patients were pneumonia (3.6%) and acute kidney injury (3.3%). Fatal adverse reactions occurred in 4.7% including pneumonia (0.7%), septic shock (0.4%), death not otherwise specified (0.4%), sudden death (0.4%), myocardial infarction (0.4%), pancreatic neoplasm (0.4%) and other infections (2.9%).

First-line treatment of metastatic or unresectable, recurrent HNSCC

The safety of KEYTRUDA, as a single agent and in combination with platinum (cisplatin or carboplatin) and FU chemotherapy, was investigated in KEYNOTE-048, a multicenter, open-label, randomized (1:1:1), active-controlled trial in patients with previously untreated, recurrent or metastatic HNSCC [see Clinical Studies (14.4)]. Patients with autoimmune disease that required systemic therapy within 2 years of treatment or a medical condition that required immunosuppression were ineligible. A total of 576 patients received KEYTRUDA 200 mg every 3 weeks either as a single agent (n=300) or in combination with platinum and FU (n=276) every 3 weeks for 6 cycles followed by KEYTRUDA, compared to 287 patients who received cetuximab weekly in combination with platinum and FU every 3 weeks for 6 cycles followed by cetuximab.

The median duration of exposure to KEYTRUDA was 3.5 months (range: 1 day to 24.2 months) in the KEYTRUDA single agent arm and was 5.8 months (range: 3 days to 24.2 months) in the combination arm. Seventeen percent of patients in the KEYTRUDA single agent arm and 18% of patients in the combination arm were exposed to KEYTRUDA for ≥12 months. Fifty-seven percent of patients receiving KEYTRUDA in combination with chemotherapy started treatment with carboplatin.

KEYTRUDA was discontinued for adverse reactions in 12% of patients in the KEYTRUDA single agent arm. The most common adverse reactions resulting in permanent discontinuation of KEYTRUDA were sepsis (1.7%) and pneumonia (1.3%). Adverse reactions leading to the interruption of KEYTRUDA occurred in 31% of patients; the most common adverse reactions leading to interruption of KEYTRUDA (≥2%) were pneumonia (2.3%), pneumonitis (2.3%), and hyponatremia (2%).

KEYTRUDA was discontinued for adverse reactions in 16% of patients in the combination arm. The most common adverse reactions resulting in permanent discontinuation of KEYTRUDA were pneumonia (2.5%), pneumonitis (1.8%), and septic shock (1.4%). Adverse reactions leading to the interruption of KEYTRUDA occurred in 45% of patients; the most common adverse reactions leading to interruption of KEYTRUDA (≥2%) were neutropenia (14%), thrombocytopenia (10%), anemia (6%), pneumonia (4.7%), and febrile neutropenia (2.9%).

Tables 18 and 19 summarize adverse reactions and laboratory abnormalities, respectively, in patients on KEYTRUDA in KEYNOTE-048.

Table 18: Adverse Reactions Occurring in ≥10% of Patients Receiving KEYTRUDA in KEYNOTE-048
 | KEYTRUDA 200 mg every 3 weeks |  | KEYTRUDA 200 mg every 3 weeks Platinum FU |  | Cetuximab Platinum FU
Adverse Reaction | n=300 |  | n=276 |  | n=287
 | All Grades [Graded per NCI CTCAE v4.0] (%) | Grades 3-4 (%) | All Grades (%) | Grades 3-4 (%) | All Grades (%) | Grades 3-4 (%)
General
Fatigue [Includes fatigue, asthenia] | 33 | 4 | 49 | 11 | 48 | 8
Pyrexia | 13 | 0.7 | 16 | 0.7 | 12 | 0
Mucosal inflammation | 4.3 | 1.3 | 31 | 10 | 28 | 5
Gastrointestinal
Constipation | 20 | 0.3 | 37 | 0 | 33 | 1.4
Nausea | 17 | 0 | 51 | 6 | 51 | 6
Diarrhea [Includes diarrhea, colitis, hemorrhagic diarrhea, microscopic colitis] | 16 | 0.7 | 29 | 3.3 | 35 | 3.1
Vomiting | 11 | 0.3 | 32 | 3.6 | 28 | 2.8
Dysphagia | 8 | 2.3 | 12 | 2.9 | 10 | 2.1
Stomatitis | 3 | 0 | 26 | 8 | 28 | 3.5
Skin
Rash [Includes dermatitis, dermatitis acneiform, dermatitis allergic, dermatitis bullous, dermatitis contact, dermatitis exfoliative, drug eruption, erythema, erythema multiforme, rash, erythematous rash, generalized rash, macular rash, maculo-papular rash, pruritic rash, seborrheic dermatitis] | 20 | 2.3 | 17 | 0.7 | 70 | 8
Pruritus | 11 | 0 | 8 | 0 | 10 | 0.3
Respiratory, Thoracic and Mediastinal
Cough [Includes cough, productive cough] | 18 | 0.3 | 22 | 0 | 15 | 0
Dyspnea [Includes dyspnea, exertional dyspnea] | 14 | 2.0 | 10 | 1.8 | 8 | 1.0
Endocrine
Hypothyroidism | 18 | 0 | 15 | 0 | 6 | 0
Metabolism and Nutrition
Decreased appetite | 15 | 1.0 | 29 | 4.7 | 30 | 3.5
Weight loss | 15 | 2 | 16 | 2.9 | 21 | 1.4
Infections
Pneumonia [Includes pneumonia, atypical pneumonia, bacterial pneumonia, staphylococcal pneumonia, aspiration pneumonia, lower respiratory tract infection, lung infection, lung infection pseudomonal] | 12 | 7 | 19 | 11 | 13 | 6
Nervous System
Headache | 12 | 0.3 | 11 | 0.7 | 8 | 0.3
Dizziness | 5 | 0.3 | 10 | 0.4 | 13 | 0.3
Peripheral sensory neuropathy [Includes peripheral sensory neuropathy, peripheral neuropathy, hypoesthesia, dysesthesia] | 1 | 0 | 14 | 1.1 | 7 | 1
Musculoskeletal
Myalgia [Includes back pain, musculoskeletal chest pain, musculoskeletal pain, myalgia] | 12 | 1.0 | 13 | 0.4 | 11 | 0.3
Neck pain | 6 | 0.7 | 10 | 1.1 | 7 | 0.7
Psychiatric
Insomnia | 7 | 0.7 | 10 | 0 | 8 | 0

Table 19: Laboratory Abnormalities Worsened from Baseline Occurring in ≥20% of Patients Receiving KEYTRUDA in KEYNOTE-048
 | KEYTRUDA 200 mg every 3 weeks |  | KEYTRUDA 200 mg every 3 weeks Platinum FU |  | Cetuximab Platinum FU
Laboratory Test [Each test incidence is based on the number of patients who had both baseline and at least one on-study laboratory measurement available: KEYTRUDA/chemotherapy (range: 240 to 267 patients), KEYTRUDA (range: 245 to 292 patients), cetuximab/chemotherapy (range: 249 to 282 patients).] | All Grades [Graded per NCI CTCAE v4.0] (%) | Grades 3-4 (%) | All Grades (%) | Grades 3-4 (%) | All Grades (%) | Grades 3-4 (%)
Hematology
Lymphopenia | 54 | 25 | 70 | 35 | 75 | 46
Anemia | 52 | 7 | 89 | 29 | 79 | 20
Thrombocytopenia | 12 | 3.8 | 73 | 18 | 76 | 18
Neutropenia | 8 | 1.4 | 68 | 37 | 73 | 43
Chemistry
Hyperglycemia | 47 | 3.8 | 54 | 6 | 65 | 4.7
Hyponatremia | 46 | 18 | 55 | 20 | 59 | 20
Hypoalbuminemia | 44 | 3.5 | 46 | 3.9 | 49 | 1.1
Increased AST | 28 | 3.1 | 25 | 1.9 | 37 | 3.6
Increased ALT | 25 | 2.1 | 22 | 1.5 | 38 | 1.8
Increased alkaline phosphatase | 25 | 2.1 | 26 | 1.1 | 33 | 1.1
Hypercalcemia | 22 | 4.5 | 16 | 4.2 | 13 | 2.5
Hypocalcemia | 22 | 1.0 | 32 | 3.8 | 58 | 6
Hyperkalemia | 21 | 2.8 | 28 | 4.2 | 29 | 4.6
Hypophosphatemia | 20 | 5 | 34 | 12 | 49 | 20
Hypokalemia | 19 | 5 | 33 | 12 | 47 | 15
Increased creatinine | 17 | 1.0 | 36 | 2.3 | 27 | 2.1
Hypomagnesemia | 15 | 0.4 | 40 | 1.7 | 76 | 9

Previously treated recurrent or metastatic HNSCC

Among the 192 patients with HNSCC enrolled in KEYNOTE-012 [see Clinical Studies (14.4)], the median duration of exposure to KEYTRUDA was 3.3 months (range: 1 day to 27.9 months). Patients with autoimmune disease or a medical condition that required immunosuppression were ineligible for KEYNOTE-012.

The study population characteristics were: median age of 60 years (range: 20 to 84), 35% age 65 or older; 83% male; and 77% White, 15% Asian, and 5% Black. Sixty-one percent of patients had two or more lines of therapy in the recurrent or metastatic setting, and 95% had prior radiation therapy. Baseline ECOG PS was 0 (30%) or 1 (70%) and 86% had M1 disease.

KEYTRUDA was discontinued due to adverse reactions in 17% of patients. Serious adverse reactions occurred in 45% of patients receiving KEYTRUDA. The most frequent serious adverse reactions reported in at least 2% of patients were pneumonia, dyspnea, confusional state, vomiting, pleural effusion, and respiratory failure. The incidence of adverse reactions, including serious adverse reactions, was similar between dosage regimens (10 mg/kg every 2 weeks or 200 mg every 3 weeks); therefore, summary safety results are provided in a pooled analysis. The most common adverse reactions (occurring in ≥20% of patients) were fatigue, decreased appetite, and dyspnea. Adverse reactions occurring in patients with HNSCC were generally similar to those occurring in 2799 patients with melanoma or NSCLC treated with KEYTRUDA as a single agent, with the exception of increased incidences of facial edema (10% all Grades; 2.1% Grades 3-4) and new or worsening hypothyroidism [see Warnings and Precautions (5.1)].

Relapsed or Refractory cHL

KEYNOTE-204

The safety of KEYTRUDA was evaluated in KEYNOTE-204 [see Clinical Studies (14.5)]. Adults with relapsed or refractory cHL received KEYTRUDA 200 mg intravenously every 3 weeks (n=148) or brentuximab vedotin (BV) 1.8 mg/kg intravenously every 3 weeks (n=152). The trial required an ANC ≥1000/µL, platelet count ≥75,000/µL, hepatic transaminases ≤2.5 times the upper limit of normal (ULN), bilirubin ≤1.5 times ULN, and ECOG performance status of 0 or 1. The trial excluded patients with active non-infectious pneumonitis, prior pneumonitis requiring steroids, active autoimmune disease, a medical condition requiring immunosuppression, or allogeneic HSCT within the past 5 years. The median duration of exposure to KEYTRUDA was 10 months (range: 1 day to 2.2 years), with 68% receiving at least 6 months of treatment and 48% receiving at least 1 year of treatment.

Serious adverse reactions occurred in 30% of patients who received KEYTRUDA. Serious adverse reactions in ≥1% included pneumonitis, pneumonia, pyrexia, myocarditis, acute kidney injury, febrile neutropenia, and sepsis. Three patients (2%) died from causes other than disease progression: two from complications after allogeneic HSCT and one from unknown cause.

Permanent discontinuation of KEYTRUDA due to an adverse reaction occurred in 14% of patients; 7% of patients discontinued treatment due to pneumonitis. Dosage interruption of KEYTRUDA due to an adverse reaction occurred in 30% of patients. Adverse reactions which required dosage interruption in ≥3% of patients were upper respiratory tract infection, pneumonitis, transaminase increase, and pneumonia.

Thirty-eight percent of patients had an adverse reaction requiring systemic corticosteroid therapy.

Table 20 summarizes adverse reactions in KEYNOTE-204.

Table 20: Adverse Reactions (≥10%) in Patients with cHL who Received KEYTRUDA in KEYNOTE-204
Adverse Reaction | KEYTRUDA 200 mg every 3 weeks N=148 |  | Brentuximab Vedotin 1.8 mg/kg every 3 weeks N=152
 | All Grades [Graded per NCI CTCAE v4.0] (%) | Grades 3- 4 (%) | All Grades (%) | Grades 3- 4 [Adverse reactions in BV arm were Grade 3 only.] (%)
Infections
Upper respiratory tract infection [Includes acute sinusitis, nasopharyngitis, pharyngitis, pharyngotonsillitis, rhinitis, sinusitis, sinusitis bacterial, tonsillitis, upper respiratory tract infection, viral upper respiratory tract infection] | 41 | 1.4 | 24 | 0
Urinary tract infection | 11 | 0 | 3 | 0.7
Musculoskeletal and Connective Tissue
Musculoskeletal pain [Includes arthralgia, back pain, bone pain, musculoskeletal discomfort, musculoskeletal chest pain, musculoskeletal pain, myalgia, neck pain, non-cardiac chest pain, pain in extremity] | 32 | 0 | 29 | 1.3
Gastrointestinal
Diarrhea [Includes diarrhea, gastroenteritis, colitis, enterocolitis] | 22 | 2.7 | 17 | 1.3
Nausea | 14 | 0 | 24 | 0.7
Vomiting | 14 | 1.4 | 20 | 0
Abdominal pain [Includes abdominal discomfort, abdominal pain, abdominal pain lower, abdominal pain upper] | 11 | 0.7 | 13 | 1.3
General
Pyrexia | 20 | 0.7 | 13 | 0.7
Fatigue [Includes fatigue, asthenia] | 20 | 0 | 22 | 0.7
Skin and Subcutaneous Tissue
Rash [Includes dermatitis acneiform, dermatitis atopic, dermatitis allergic, dermatitis contact, dermatitis exfoliative, dermatitis psoriasiform, eczema, rash, rash erythematous, rash follicular‚ rash maculo-papular, rash papular, rash pruritic, toxic skin eruption] | 20 | 0 | 19 | 0.7
Pruritus | 18 | 0 | 12 | 0
Respiratory, Thoracic and Mediastinal
Cough [Includes cough, productive cough] | 20 | 0.7 | 14 | 0.7
Pneumonitis [Includes pneumonitis, interstitial lung disease] | 11 | 5 | 3 | 1.3
Dyspnea [Includes dyspnea, dyspnea exertional, wheezing] | 11 | 0.7 | 7 | 0.7
Endocrine
Hypothyroidism | 19 | 0 | 3 | 0
Nervous System
Peripheral neuropathy [Includes dysesthesia, hypoesthesia, neuropathy peripheral, paraesthesia, peripheral motor neuropathy, peripheral sensorimotor neuropathy, peripheral sensory neuropathy, polyneuropathy] | 11 | 0.7 | 43 | 7
Headache [Includes headache, migraine, tension headache] | 11 | 0 | 11 | 0

Clinically relevant adverse reactions in <10% of patients who received KEYTRUDA included herpes virus infection (9%), pneumonia (8%), oropharyngeal pain (8%), hyperthyroidism (5%), hypersensitivity (4.1%), infusion reactions (3.4%), altered mental state (2.7%), and in 1.4% each, uveitis, myocarditis, thyroiditis, febrile neutropenia, sepsis, and tumor flare.

Table 21 summarizes laboratory abnormalities in KEYNOTE-204.

Table 21: Laboratory Abnormalities (≥15%) That Worsened from Baseline in Patients with cHL in KEYNOTE-204
Laboratory Abnormality [Each test incidence is based on the number of patients who had both baseline and at least one on-study laboratory measurement available: KEYTRUDA (range: 143 to 148 patients) and BV (range: 145 to 152 patients); hypomagnesemia: KEYTRUDA n=52 and BV n=47.] | KEYTRUDA 200 mg every 3 weeks |  | Brentuximab Vedotin 1.8 mg/kg every 3 weeks
 | All Grades [Graded per NCI CTCAE v4.0] (%) | Grades 3-4 (%) | All Grades (%) | Grades 3-4 (%)
Chemistry
Hyperglycemia | 45 | 4.1 | 36 | 2.0
Increased AST | 38 | 4.7 | 38 | 2.0
Increased ALT | 31 | 5 | 43 | 2.6
Hypophosphatemia | 31 | 4.9 | 17 | 2.8
Increased creatinine | 26 | 3.4 | 13 | 2.6
Hypomagnesemia | 23 | 0 | 13 | 0
Hyponatremia | 24 | 4.1 | 20 | 3.3
Hypocalcemia | 21 | 2.0 | 15 | 0
Increased alkaline phosphatase | 19 | 2.1 | 21 | 2.0
Hypoalbuminemia | 16 | 0.7 | 18 | 0.7
Hyperbilirubinemia | 15 | 1.4 | 8 | 0.7
Hematology
Lymphopenia | 34 | 8 | 32 | 13
Thrombocytopenia | 32 | 9 | 24 | 4.0
Neutropenia | 27 | 8 | 42 | 16
Anemia | 22 | 4.1 | 32 | 7

KEYNOTE-087

Among the 210 patients with cHL who received KEYTRUDA in KEYNOTE-087 [see Clinical Studies (14.5)], the median duration of exposure to KEYTRUDA was 8.4 months (range: 1 day to 15.2 months). Serious adverse reactions occurred in 16% of patients who received KEYTRUDA. Serious adverse reactions that occurred in ≥1% of patients included pneumonia, pneumonitis, pyrexia, dyspnea, graft versus host disease (GVHD) and herpes zoster. Two patients died from causes other than disease progression; one from GVHD after subsequent allogeneic HSCT and one from septic shock.

Permanent discontinuation of KEYTRUDA due to an adverse reaction occurred in 5% of patients and dosage interruption due to an adverse reaction occurred in 26%. Fifteen percent of patients had an adverse reaction requiring systemic corticosteroid therapy. Tables 22 and 23 summarize adverse reactions and laboratory abnormalities, respectively, in KEYNOTE-087.

Table 22: Adverse Reactions (≥10%) in Patients with cHL who Received KEYTRUDA in KEYNOTE-087
Adverse Reaction | KEYTRUDA 200 mg every 3 weeks N=210
 | All Grades [Graded per NCI CTCAE v4.0] (%) | Grade 3 (%)
General
Fatigue [Includes fatigue, asthenia] | 26 | 1.0
Pyrexia | 24 | 1.0
Respiratory, Thoracic and Mediastinal
Cough [Includes cough, productive cough] | 24 | 0.5
Dyspnea [Includes dyspnea, dyspnea exertional, wheezing] | 11 | 1.0
Musculoskeletal and Connective Tissue
Musculoskeletal pain [Includes back pain, myalgia, bone pain, musculoskeletal pain, pain in extremity, musculoskeletal chest pain, musculoskeletal discomfort, neck pain] | 21 | 1.0
Arthralgia | 10 | 0.5
Gastrointestinal
Diarrhea [Includes diarrhea, gastroenteritis, colitis, enterocolitis] | 20 | 1.4
Vomiting | 15 | 0
Nausea | 13 | 0
Skin and Subcutaneous Tissue
Rash [Includes rash, rash maculo-papular, drug eruption, eczema, eczema asteatotic, dermatitis, dermatitis acneiform, dermatitis contact, rash erythematous, rash macular, rash papular, rash pruritic, seborrheic dermatitis, dermatitis psoriasiform] | 20 | 0.5
Pruritus | 11 | 0
Endocrine
Hypothyroidism | 14 | 0.5
Infections
Upper respiratory tract infection | 13 | 0
Nervous System
Headache | 11 | 0.5
Peripheral neuropathy [Includes neuropathy peripheral, peripheral sensory neuropathy, hypoesthesia, paresthesia, dysesthesia, polyneuropathy] | 10 | 0

Clinically relevant adverse reactions in <10% of patients who received KEYTRUDA included infusion reactions (9%), hyperthyroidism (3%), pneumonitis (3%), uveitis and myositis (1% each), and myelitis and myocarditis (0.5% each).

Table 23: Select Laboratory Abnormalities (≥15%) That Worsened from Baseline in Patients with cHL who Received KEYTRUDA in KEYNOTE-087
Laboratory Abnormality [Each test incidence is based on the number of patients who had both baseline and at least one on-study laboratory measurement available: KEYTRUDA (range: 208 to 209 patients)] | KEYTRUDA 200 mg every 3 weeks
 | All Grades [Graded per NCI CTCAE v4.0] (%) | Grades 3-4 (%)
Chemistry
Hypertransaminasemia [Includes elevation of AST or ALT] | 35 | 2.4
Increased alkaline phosphatase | 17 | 0
Increased creatinine | 15 | 0.5
Hematology
Anemia | 30 | 6
Thrombocytopenia | 27 | 4.3
Neutropenia | 25 | 7

Hyperbilirubinemia occurred in less than 15% of patients on KEYNOTE-087 (10% all Grades, 2.4% Grade 3-4).

PMBCL

Among the 53 patients with PMBCL who received KEYTRUDA in KEYNOTE-170 [see Clinical Studies (14.6)], the median duration of exposure to KEYTRUDA was 3.5 months (range: 1 day to 22.8 months). Serious adverse reactions occurred in 26% of patients. Serious adverse reactions that occurred in >2% of patients included arrhythmia (4%), cardiac tamponade (2%), myocardial infarction (2%), pericardial effusion (2%), and pericarditis (2%). Six (11%) patients died within 30 days of start of treatment. Permanent discontinuation of KEYTRUDA due to an adverse reaction occurred in 8% of patients and dosage interruption due to an adverse reaction occurred in 15%. Twenty-five percent of patients had an adverse reaction requiring systemic corticosteroid therapy. Tables 24 and 25 summarize adverse reactions and laboratory abnormalities, respectively, in KEYNOTE-170.

Table 24: Adverse Reactions (≥10%) in Patients with PMBCL who Received KEYTRUDA in KEYNOTE-170
Adverse Reaction | KEYTRUDA 200 mg every 3 weeks N=53
 | All Grades [Graded per NCI CTCAE v4.0] (%) | Grades 3-4 (%)
Musculoskeletal and Connective Tissue
Musculoskeletal pain [Includes arthralgia, back pain, myalgia, musculoskeletal pain, pain in extremity, musculoskeletal chest pain, bone pain, neck pain, non-cardiac chest pain] | 30 | 0
Infections
Upper respiratory tract infection [Includes nasopharyngitis, pharyngitis, rhinorrhea, rhinitis, sinusitis, upper respiratory tract infection] | 28 | 0
General
Pyrexia | 28 | 0
Fatigue [Includes fatigue, asthenia] | 23 | 2
Respiratory, Thoracic and Mediastinal
Cough [Includes allergic cough, cough, productive cough] | 26 | 2
Dyspnea | 21 | 11
Gastrointestinal
Diarrhea [Includes diarrhea, gastroenteritis] | 13 | 2
Abdominal pain [Includes abdominal pain, abdominal pain upper] | 13 | 0
Nausea | 11 | 0
Cardiac
Arrhythmia [Includes atrial fibrillation, sinus tachycardia, supraventricular tachycardia, tachycardia] | 11 | 4
Nervous System
Headache | 11 | 0

Clinically relevant adverse reactions in <10% of patients who received KEYTRUDA included hypothyroidism (8%), hyperthyroidism and pericarditis (4% each), and thyroiditis, pericardial effusion, pneumonitis, arthritis and acute kidney injury (2% each).

Table 25: Laboratory Abnormalities (≥15%) That Worsened from Baseline in Patients with PMBCL who Received KEYTRUDA in KEYNOTE-170
Laboratory Abnormality [Each test incidence is based on the number of patients who had both baseline and at least one on-study laboratory measurement available: KEYTRUDA (range: 41 to 45 patients)] | KEYTRUDA 200 mg every 3 weeks
 | All Grades [Graded per NCI CTCAE v4.0] (%) | Grades 3-4 (%)
Hematology
Anemia | 23 | 0
Leukopenia | 47 | 12
Lymphopenia | 27 | 10
Neutropenia | 39 | 15
Chemistry
Hyperglycemia | 33 | 2.2
Hypophosphatemia | 24 | 11
Hypertransaminasemia [Includes elevation of AST or ALT] | 24 | 4.4
Hypoglycemia | 20 | 0
Increased creatinine | 16 | 0

Urothelial Cancer

Patients with urothelial cancer in combination with enfortumab vedotin

The safety of KEYTRUDA in combination with enfortumab vedotin was investigated in KEYNOTE-A39 in patients with locally advanced or metastatic urothelial cancer [see Clinical Studies (14.7)]. A total of 440 patients received KEYTRUDA 200 mg on Day 1 and enfortumab vedotin 1.25 mg/kg on Days 1 and 8 of each 21-day cycle compared to 433 patients who received gemcitabine on Days 1 and 8 and investigator’s choice of cisplatin or carboplatin on Day 1 of each 21-day cycle. Among patients who received KEYTRUDA and enfortumab vedotin, the median duration of exposure to KEYTRUDA was 8.5 months (range: 9 days to 28.5 months).

Fatal adverse reactions occurred in 3.9% of patients treated with KEYTRUDA in combination with enfortumab vedotin including acute respiratory failure (0.7%), pneumonia (0.5%), and pneumonitis/ILD (0.2%).

Serious adverse reactions occurred in 50% of patients receiving KEYTRUDA in combination with enfortumab vedotin. Serious adverse reactions in ≥2% of patients receiving KEYTRUDA in combination with enfortumab vedotin were rash (6%), acute kidney injury (5%), pneumonitis/ILD (4.5%), urinary tract infection (3.6%), diarrhea (3.2%), pneumonia (2.3%), pyrexia (2%), and hyperglycemia (2%).

Permanent discontinuation of KEYTRUDA occurred in 27% of patients. The most common adverse reactions (≥2%) resulting in permanent discontinuation of KEYTRUDA were pneumonitis/ILD (4.8%) and rash (3.4%).

Dose interruptions of KEYTRUDA occurred in 61% of patients. The most common adverse reactions (≥2%) resulting in interruption of KEYTRUDA were rash (17%), peripheral neuropathy (7%), COVID-19 (5%), diarrhea (4.3%), pneumonitis/ILD (3.6%), neutropenia (3.4%), fatigue (3%), alanine aminotransferase increased (2.7%), hyperglycemia (2.5%), pneumonia (2%), and pruritus (2%).

Tables 26 and 27 summarize adverse reactions and laboratory abnormalities, respectively, in patients on KEYTRUDA in combination with enfortumab vedotin in KEYNOTE-A39.

Table 26: Adverse Reactions ≥20% (All Grades) in Patients Treated with KEYTRUDA in Combination with Enfortumab Vedotin in KEYNOTE-A39
Adverse Reaction | KEYTRUDA in combination with Enfortumab Vedotin n=440 |  | Chemotherapy n=433
Adverse Reaction | All Grades [Graded per NCI CTCAE v4.03] % | Grades 3-4 % | All Grades % | Grades 3-4 %
Skin and subcutaneous tissue disorders
Rash [Includes multiple terms] | 68 | 15 | 15 | 0
Pruritus | 41 | 1.1 | 7 | 0
Alopecia | 35 | 0.5 | 8 | 0.2
General disorders and administration site conditions
Fatigue | 51 | 6 | 57 | 7
Nervous system disorders
Peripheral neuropathy | 67 | 8 | 14 | 0
Dysgeusia | 21 | 0 | 9 | 0
Metabolism and nutrition disorders
Decreased appetite | 33 | 1.8 | 26 | 1.8
Gastrointestinal disorders
Diarrhea | 38 | 4.5 | 16 | 1.4
Nausea | 26 | 1.6 | 41 | 2.8
Constipation | 26 | 0 | 34 | 0.7
Investigations
Weight loss | 33 | 3.6 | 9 | 0.2
Eye disorders
Dry eye | 24 | 0 | 2.1 | 0
Infections and infestations
Urinary tract infection | 21 | 5 | 19 | 8

Clinically relevant adverse reactions (<20%) include pyrexia (18%), dry skin (17%), vomiting (12%), pneumonitis/ILD (10%), hypothyroidism (10%), blurred vision (6%), infusion site extravasation (2%), and myositis (0.5%).

Table 27: Selected Laboratory Abnormalities Worsened from Baseline Occurring in ≥20% of Patients in KEYNOTE-A39
Laboratory Test [Each test incidence is based on the number of patients who had both baseline and at least one on-study laboratory measurement available: KEYTRUDA (range: 407 to 439 patients)] | KEYTRUDA 200 mg every 3 weeks and Enfortumab Vedotin |  | Chemotherapy
Laboratory Test [Each test incidence is based on the number of patients who had both baseline and at least one on-study laboratory measurement available: KEYTRUDA (range: 407 to 439 patients)] | All Grades [Graded per NCI CTCAE v4.03] % | Grades 3-4 % | All Grades % | Grades 3-4 %
Chemistry
Increased aspartate aminotransferase | 75 | 4.6 | 39 | 3.3
Increased creatinine | 71 | 3.2 | 68 | 2.6
Hyperglycemia | 66 | 14 | 54 | 4.7
Increased alanine aminotransferase | 59 | 5 | 49 | 3.3
Hyponatremia | 46 | 13 | 47 | 13
Hypophosphatemia | 44 | 9 | 36 | 9
Hypoalbuminemia | 39 | 1.8 | 35 | 0.5
Hypokalemia | 26 | 5 | 16 | 3.1
Hyperkalemia | 24 | 1.4 | 36 | 4.0
Hypercalcemia | 21 | 1.2 | 14 | 0.2
Hematology
Lymphopenia | 58 | 15 | 59 | 17
Anemia | 53 | 7 | 89 | 33
Neutropenia | 30 | 9 | 80 | 50

Cisplatin-ineligible patients with urothelial cancer in combination with enfortumab vedotin

The safety of KEYTRUDA in combination with enfortumab vedotin was investigated in KEYNOTE-869 in patients with locally advanced or metastatic urothelial cancer and who are not eligible for cisplatin-based chemotherapy [see Clinical Studies (14.7)]. A total of 121 patients received KEYTRUDA 200 mg on Day 1, and enfortumab vedotin 1.25 mg/kg on days 1 and 8 of each 21-day cycle. The median duration of exposure to KEYTRUDA was 6.9 months (range 1 day to 29.6 months).

Fatal adverse reactions occurred in 5% of patients treated with KEYTRUDA in combination with enfortumab vedotin, including sepsis (1.6%), bullous dermatitis (0.8%), myasthenia gravis (0.8%), and pneumonitis (0.8%).

Serious adverse reactions occurred in 50% of patients receiving KEYTRUDA and enfortumab vedotin. Serious adverse reactions in ≥2% of patients receiving KEYTRUDA in combination with enfortumab vedotin were acute kidney injury (7%), urinary tract infection (7%), urosepsis (5%), hematuria (3.3%), pneumonia (3.3%), pneumonitis (3.3%), sepsis (3.3%), anemia (2.5%), diarrhea (2.5%), hypotension (2.5%), myasthenia gravis (2.5%), myositis (2.5%), and urinary retention (2.5%).

Permanent discontinuation of KEYTRUDA occurred in 32% of patients. The most common adverse reactions (≥2%) resulting in permanent discontinuation of KEYTRUDA were pneumonitis (5%), peripheral neuropathy (5%), rash (3.3%), and myasthenia gravis (2.5%).

Dose interruptions of KEYTRUDA occurred in 69% of patients. The most common adverse reactions (≥2%) resulting in interruption of KEYTRUDA were peripheral neuropathy (22%), rash (17%), neutropenia (7%), fatigue (6%), diarrhea (5%), lipase increased (5%), acute kidney injury (3.3%), ALT increased (2.5%), and COVID-19 (2.5%).

Tables 28 and 29 summarize adverse reactions and laboratory abnormalities, respectively, in patients on KEYTRUDA in combination with enfortumab vedotin in KEYNOTE-869.

Table 28: Adverse Reactions Occurring in ≥20% of Patients Treated with KEYTRUDA in Combination with Enfortumab Vedotin in KEYNOTE-869
Adverse Reaction | KEYTRUDA in combination with Enfortumab Vedotin n=121
Adverse Reaction | All Grades [Graded per NCI CTCAE v4.03] % | Grade 3-4 %
Skin and subcutaneous tissue disorders
Rash [Includes: blister, conjunctivitis, dermatitis, dermatitis bullous, dermatitis exfoliative generalized, erythema, erythema multiforme, exfoliative rash, palmar-plantar erythrodysesthesia syndrome, pemphigoid, rash, rash erythematous, rash macular, rash maculo-papular, rash papular, rash pruritic, rash vesicular, skin exfoliation, and stomatitis] | 71 | 21
Alopecia | 52 | 0
Pruritus | 40 | 3.3
Dry skin | 21 | 0.8
Nervous system disorders
Peripheral neuropathy [Includes: dysesthesia, hypoesthesia, muscular weakness, paresthesia, peripheral motor neuropathy, peripheral sensorimotor neuropathy, peripheral sensory neuropathy, and gait disturbance] | 65 | 3.3
Dysgeusia | 35 | 0
Dizziness | 23 | 0
General disorders and administration site conditions
Fatigue | 60 | 11
Peripheral edema | 26 | 0
Investigations
Weight loss | 48 | 5
Gastrointestinal disorders
Diarrhea | 45 | 7
Nausea | 36 | 0.8
Constipation | 27 | 0
Metabolism and nutrition disorders
Decreased appetite | 38 | 0.8
Infections and infestations
Urinary tract infection | 30 | 12
Eye disorders
Dry eye | 25 | 0
Musculoskeletal and connective tissue disorders
Arthralgia | 23 | 1.7

Clinically relevant adverse reactions (<20%) include vomiting (19.8%), fever (18%), hypothyroidism (11%), pneumonitis/ILD (10%), myositis (3.3%), myasthenia gravis (2.5%), and infusion site extravasation (0.8%).

Table 29: Selected Laboratory Abnormalities Worsened from Baseline Occurring in ≥20% of Patients in KEYNOTE-869
Laboratory Test [Each test incidence is based on the number of patients who had both baseline and at least one on-study laboratory measurement available: KEYTRUDA (range: 114 to 121 patients)] | KEYTRUDA 200 mg every 3 weeks and Enfortumab Vedotin
Laboratory Test [Each test incidence is based on the number of patients who had both baseline and at least one on-study laboratory measurement available: KEYTRUDA (range: 114 to 121 patients)] | All Grades [Graded per NCI CTCAE v4.03] % | Grades 3-4 %
Chemistry
Hyperglycemia | 74 | 13
Increased aspartate aminotransferase | 73 | 9
Increased creatinine | 69 | 3.3
Hyponatremia | 60 | 19
Increased alanine aminotransferase | 60 | 7
Increased lipase | 59 | 32
Hypoalbuminemia | 59 | 4.2
Hypophosphatemia | 51 | 15
Hypokalemia | 35 | 8
Increased potassium | 27 | 1.7
Increased calcium | 27 | 4.2
Hematology
Anemia | 69 | 15
Lymphopenia | 64 | 17
Neutropenia | 32 | 12

Platinum-Ineligible Patients with Urothelial Carcinoma

The safety of KEYTRUDA was investigated in KEYNOTE-052, a single-arm trial that enrolled 370 patients with locally advanced or metastatic urothelial carcinoma who had one or more comorbidities. Patients with autoimmune disease or medical conditions that required systemic corticosteroids or other immunosuppressive medications were ineligible [see Clinical Studies (14.7)]. Patients received KEYTRUDA 200 mg every 3 weeks until unacceptable toxicity or either radiographic or clinical disease progression.

The median duration of exposure to KEYTRUDA was 2.8 months (range: 1 day to 15.8 months).

KEYTRUDA was discontinued due to adverse reactions in 11% of patients. Eighteen patients (5%) died from causes other than disease progression. Five patients (1.4%) who were treated with KEYTRUDA experienced sepsis which led to death, and three patients (0.8%) experienced pneumonia which led to death. Adverse reactions leading to interruption of KEYTRUDA occurred in 22% of patients; the most common (≥1%) were liver enzyme increase, diarrhea, urinary tract infection, acute kidney injury, fatigue, joint pain, and pneumonia. Serious adverse reactions occurred in 42% of patients. The most frequent serious adverse reactions (≥2%) were urinary tract infection, hematuria, acute kidney injury, pneumonia, and urosepsis.

Immune-related adverse reactions that required systemic glucocorticoids occurred in 8% of patients, use of hormonal supplementation due to an immune-related adverse reaction occurred in 8% of patients, and 5% of patients required at least one steroid dose ≥40 mg oral prednisone equivalent.

Table 30 summarizes adverse reactions in patients on KEYTRUDA in KEYNOTE-052.

Table 30: Adverse Reactions Occurring in ≥10% of Patients Receiving KEYTRUDA in KEYNOTE-052
Adverse Reaction | KEYTRUDA 200 mg every 3 weeks N=370
 | All Grades [Graded per NCI CTCAE v4.0] (%) | Grades 3–4 (%)
General
Fatigue [Includes fatigue, asthenia] | 38 | 6
Pyrexia | 11 | 0.5
Weight loss | 10 | 0
Musculoskeletal and Connective Tissue
Musculoskeletal pain [Includes back pain, bone pain, musculoskeletal chest pain, musculoskeletal pain, myalgia, neck pain, pain in extremity, spinal pain] | 24 | 4.9
Arthralgia | 10 | 1.1
Metabolism and Nutrition
Decreased appetite | 22 | 1.6
Hyponatremia | 10 | 4.1
Gastrointestinal
Constipation | 21 | 1.1
Diarrhea [Includes diarrhea, colitis, enterocolitis, gastroenteritis, frequent bowel movements] | 20 | 2.4
Nausea | 18 | 1.1
Abdominal pain [Includes abdominal pain, pelvic pain, flank pain, abdominal pain lower, tumor pain, bladder pain, hepatic pain, suprapubic pain, abdominal discomfort, abdominal pain upper] | 18 | 2.7
Elevated LFTs [Includes autoimmune hepatitis, hepatitis, hepatitis toxic, liver injury, increased transaminases, hyperbilirubinemia, increased blood bilirubin, increased alanine aminotransferase, increased aspartate aminotransferase, increased hepatic enzymes, increased liver function tests] | 13 | 3.5
Vomiting | 12 | 0
Skin and Subcutaneous Tissue
Rash [Includes dermatitis, dermatitis bullous, eczema, erythema, rash, rash macular, rash maculo-papular, rash pruritic, rash pustular, skin reaction, dermatitis acneiform, seborrheic dermatitis, palmar-plantar erythrodysesthesia syndrome, rash generalized] | 21 | 0.5
Pruritus | 19 | 0.3
Edema peripheral [Includes edema peripheral, peripheral swelling] | 14 | 1.1
Infections
Urinary tract infection | 19 | 9
Blood and Lymphatic System
Anemia | 17 | 7
Respiratory, Thoracic, and Mediastinal
Cough | 14 | 0
Dyspnea | 11 | 0.5
Renal and Urinary
Increased blood creatinine | 11 | 1.1
Hematuria | 13 | 3.0

Previously Treated Urothelial Carcinoma

The safety of KEYTRUDA for the treatment of patients with locally advanced or metastatic urothelial carcinoma with disease progression following platinum-containing chemotherapy was investigated in KEYNOTE-045. KEYNOTE-045 was a multicenter, open-label, randomized (1:1), active-controlled trial in which 266 patients received KEYTRUDA 200 mg every 3 weeks or investigator's choice of chemotherapy (n=255), consisting of paclitaxel (n=84), docetaxel (n=84) or vinflunine (n=87) [see Clinical Studies (14.7)]. Patients with autoimmune disease or a medical condition that required systemic corticosteroids or other immunosuppressive medications were ineligible.

The median duration of exposure was 3.5 months (range: 1 day to 20 months) in patients who received KEYTRUDA and 1.5 months (range: 1 day to 14 months) in patients who received chemotherapy.

KEYTRUDA was discontinued due to adverse reactions in 8% of patients. The most common adverse reaction resulting in permanent discontinuation of KEYTRUDA was pneumonitis (1.9%). Adverse reactions leading to interruption of KEYTRUDA occurred in 20% of patients; the most common (≥1%) were urinary tract infection (1.5%), diarrhea (1.5%), and colitis (1.1%). Serious adverse reactions occurred in 39% of KEYTRUDA-treated patients. The most frequent serious adverse reactions (≥2%) in KEYTRUDA-treated patients were urinary tract infection, pneumonia, anemia, and pneumonitis. Tables 31 and 32 summarize adverse reactions and laboratory abnormalities, respectively, in patients on KEYTRUDA in KEYNOTE-045.

Table 31: Adverse Reactions Occurring in ≥10% of Patients Receiving KEYTRUDA in KEYNOTE-045
Adverse Reaction | KEYTRUDA 200 mg every 3 weeks |  | Chemotherapy [Chemotherapy: paclitaxel, docetaxel, or vinflunine]
Adverse Reaction | n=266 |  | n=255
 | All Grades [Graded per NCI CTCAE v4.0] (%) | Grades 3-4 (%) | All Grades (%) | Grades 3-4 (%)
General
Fatigue [Includes asthenia, fatigue, malaise, lethargy] | 38 | 4.5 | 56 | 11
Pyrexia | 14 | 0.8 | 13 | 1.2
Musculoskeletal and Connective Tissue
Musculoskeletal pain [Includes back pain, myalgia, bone pain, musculoskeletal pain, pain in extremity, musculoskeletal chest pain, musculoskeletal discomfort, neck pain] | 32 | 3.0 | 27 | 2.0
Skin and Subcutaneous Tissue
Pruritus | 23 | 0 | 6 | 0.4
Rash [Includes rash maculo-papular, rash, genital rash, rash erythematous, rash papular, rash pruritic, rash pustular, erythema, drug eruption, eczema, eczema asteatotic, dermatitis contact, dermatitis acneiform, dermatitis, seborrheic keratosis, lichenoid keratosis] | 20 | 0.4 | 13 | 0.4
Gastrointestinal
Nausea | 21 | 1.1 | 29 | 1.6
Constipation | 19 | 1.1 | 32 | 3.1
Diarrhea [Includes diarrhea, gastroenteritis, colitis, enterocolitis] | 18 | 2.3 | 19 | 1.6
Vomiting | 15 | 0.4 | 13 | 0.4
Abdominal pain | 13 | 1.1 | 13 | 2.7
Infections
Urinary tract infection | 15 | 4.9 | 14 | 4.3
Metabolism and Nutrition
Decreased appetite | 21 | 3.8 | 21 | 1.2
Respiratory, Thoracic and Mediastinal
Cough [Includes cough, productive cough] | 15 | 0.4 | 9 | 0
Dyspnea [Includes dyspnea, dyspnea exertional, wheezing] | 14 | 1.9 | 12 | 1.2
Renal and Urinary
Hematuria [Includes blood urine present, hematuria, chromaturia] | 12 | 2.3 | 8 | 1.6

Table 32: Laboratory Abnormalities Worsened from Baseline Occurring in ≥20% of Urothelial Carcinoma Patients Receiving KEYTRUDA in KEYNOTE-045
Laboratory Test [Each test incidence is based on the number of patients who had both baseline and at least one on-study laboratory measurement available: KEYTRUDA (range: 240 to 248 patients) and chemotherapy (range: 238 to 244 patients); phosphate decreased: KEYTRUDA n=232 and chemotherapy n=222.] | KEYTRUDA 200 mg every 3 weeks |  | Chemotherapy
 | All Grades [Graded per NCI CTCAE v4.0] % | Grades 3-4 % | All Grades % | Grades 3-4 %
Chemistry
Hyperglycemia | 52 | 8 | 60 | 7
Anemia | 52 | 13 | 68 | 18
Lymphopenia | 45 | 15 | 55 | 26
Hypoalbuminemia | 43 | 1.7 | 50 | 3.8
Hyponatremia | 37 | 9 | 47 | 13
Increased alkaline phosphatase | 37 | 7 | 33 | 4.9
Increased creatinine | 35 | 4.4 | 28 | 2.9
Hypophosphatemia | 29 | 8 | 34 | 14
Increased AST | 28 | 4.1 | 20 | 2.5
Hyperkalemia | 28 | 0.8 | 27 | 6
Hypocalcemia | 26 | 1.6 | 34 | 2.1

Neoadjuvant and Adjuvant Treatment of Cisplatin-Ineligible Patients with MIBC in Combination with Enfortumab Vedotin

The safety of KEYTRUDA in combination with enfortumab vedotin as neoadjuvant treatment and continued after radical cystectomy (RC) as adjuvant treatment was investigated in KEYNOTE-905, an open-label, multicenter, randomized, active-controlled trial in patients with previously untreated MIBC who were ineligible for or declined cisplatin-based chemotherapy. Patients received KEYTRUDA in combination with enfortumab vedotin (n=167) before and after RC with pelvic lymph node dissection (PLND) or RC with PLND alone (n=159) [see Clinical Studies (14.7)].

For the 167 patients who received KEYTRUDA in the neoadjuvant phase, the median duration of exposure to KEYTRUDA 200 mg every 3 weeks was 1.4 months (range: 1 day to 2.7 months) and the median number of cycles of KEYTRUDA was 3 (range: 1 to 3) out of the planned 3 cycles in the neoadjuvant phase. For the 96 patients who received KEYTRUDA in the adjuvant phase, the median duration of exposure to KEYTRUDA 200 mg every 3 weeks was 8.5 months (range: 1 day to 12.9 months) and the median number of cycles of KEYTRUDA was 12 (range: 1 to 14) out of the planned 14 cycles in the adjuvant phase. Across the combined neoadjuvant and adjuvant phases (n=167), the median number of cycles of KEYTRUDA was 5 (range: 1 to 17) out of the planned 17 cycles.

Tables 33 and 34 summarize adverse reactions and laboratory abnormalities, respectively, in patients on KEYTRUDA in combination with enfortumab vedotin in KEYNOTE-905.

Table 33: Adverse Reactions ≥20% (All Grades) in Patients Treated with KEYTRUDA in Combination with Enfortumab Vedotin in KEYNOTE-905
Adverse Reaction | KEYTRUDA 200 mg every 3 weeks in combination with enfortumab vedotin before and after RC with PLND n=167 |  | RC with PLND alone n=159
Adverse Reaction | All Grades % | Grade 3-4 % | All Grades % | Grade 3-4 %
Skin and subcutaneous tissue disorders
Rash [Includes multiple terms.] , [Includes rash, rash maculo-papular, conjunctivitis, erythema, eczema, skin exfoliation, palmar-plantar erythrodysesthesia syndrome, blister, dermatitis, dermatitis exfoliative generalized, exfoliative rash, rash papular, rash pruritic, dermatitis bullous, drug eruption, pemphigoid, rash vesicular, and dermatitis contact.] | 54 | 7 | 1.3 | 0
Pruritus | 47 | 3 | 0 | 0
Alopecia | 35 | 0.6 | 0 | 0
General disorders and administration site conditions
Fatigue | 47 | 4.2 | 6 | 0.6
Nervous system disorders
Peripheral neuropathy | 39 | 3 | 1.9 | 0
Dysgeusia | 35 | 0 | 0 | 0
Gastrointestinal disorders
Diarrhea | 34 | 5 | 3.1 | 1.3
Constipation | 28 | 1.8 | 8 | 0
Nausea | 26 | 1.2 | 8 | 0.6
Metabolism and nutrition disorders
Decreased appetite | 28 | 0.6 | 1.9 | 0
Infections and infestations
Urinary tract infection | 24 | 12 | 13 | 11
Eye disorders
Dry eye | 21 | 0 | 0 | 0
Investigations
Weight loss | 20 | 0 | 3.1 | 0

Clinically relevant adverse reactions (<20%) include dry skin (15%), hypothyroidism (14%), vomiting (9%), pneumonitis/ILD (4.2%), skin hyperpigmentation (3.0%), infusion site extravasation (1.2%), and myasthenia gravis and myositis (0.6% each).

Table 34: Selected Laboratory Abnormalities Worsened from Baseline Occurring in ≥20% of Patients Treated with KEYTRUDA in Combination with Enfortumab Vedotin in KEYNOTE-905
Laboratory Test [Each test incidence is based on the number of patients who had both baseline and at least one on-study laboratory measurement available: KEYTRUDA in combination with enfortumab vedotin (167 patients), and RC and PLND alone (range: 110 to 121 patients).] | KEYTRUDA 200 mg every 3 weeks in combination with enfortumab vedotin before and after RC with PLND n=167 |  | RC with PLND alone n=159
Laboratory Test [Each test incidence is based on the number of patients who had both baseline and at least one on-study laboratory measurement available: KEYTRUDA in combination with enfortumab vedotin (167 patients), and RC and PLND alone (range: 110 to 121 patients).] | All Grades [Graded per NCI CTCAE v4.03] % | Grades 3-4 % | All Grades % | Grades 3-4 %
Chemistry
Increased glucose | 72 | 12 | 24 | 1.7
Increased AST | 55 | 6 | 11 | 1.8
Increased ALT | 53 | 4.8 | 13 | 0.9
Increased creatinine | 47 | 8 | 31 | 2.5
Decreased sodium | 44 | 13 | 18 | 7
Increased potassium | 39 | 7 | 20 | 6
Decreased phosphate | 26 | 6 | 1.8 | 0
Hematology
Decreased hemoglobin | 60 | 13 | 48 | 8
Decreased lymphocytes | 40 | 8 | 17 | 1.7
ALT = alanine aminotransferase; AST = aspartate aminotransferase.

Neoadjuvant Phase of KEYNOTE-905

A total of 167 patients received at least 1 dose of KEYTRUDA in combination with enfortumab vedotin as neoadjuvant treatment before receiving RC.

In the neoadjuvant phase, serious adverse reactions occurred in 27% of patients receiving KEYTRUDA in combination with enfortumab vedotin. The most frequent (≥2%) serious adverse reactions were urinary tract infection (3.6%) and hematuria (2.4%). Fatal adverse reactions occurred in 1.2% of patients, including myasthenia gravis and toxic epidermal necrolysis (0.6% each). Additional fatal adverse reactions were reported in 2.7% of patients in the post-surgery phase before adjuvant treatment started, including sepsis and intestinal obstruction (1.4% each).

Permanent discontinuation of KEYTRUDA due to an adverse reaction occurred in 15% of patients. The most frequent (>1%) adverse reactions resulting in permanent discontinuation of KEYTRUDA were rash (2.4%, including generalized exfoliative dermatitis), increased alanine aminotransferase, increased aspartate aminotransferase, diarrhea, dysgeusia, and toxic epidermal necrolysis (1.2% each).

Adverse reactions leading to dose interruption of KEYTRUDA in the neoadjuvant phase occurred in 20% of patients. The most common adverse reactions (≥2%) leading to dose interruption of KEYTRUDA were rash (4.8%) and neutropenia (2.4%). Of the 167 patients in the KEYTRUDA in combination with enfortumab vedotin arm who received neoadjuvant treatment, 7 (4.2%) patients did not receive surgery due to adverse reactions. The adverse reactions that led to cancellation of surgery were acute myocardial infarction, bile duct cancer, colon cancer, respiratory distress, urinary tract infection, and the two deaths due to myasthenia gravis and toxic epidermal necrolysis (0.6% each).

Of the 146 patients who received neoadjuvant treatment with KEYTRUDA in combination with enfortumab vedotin and underwent radical cystectomy, 6 (4.1%) patients experienced delay of surgery (defined as time from last neoadjuvant treatment to surgery exceeding 8 weeks) due to adverse reactions.

Adjuvant Phase of KEYNOTE-905

Patients who did not proceed to surgery were ineligible for adjuvant therapy. Of the 149 patients who underwent surgery, 100 patients received adjuvant treatment with KEYTRUDA in combination with enfortumab vedotin. Of the 49 patients who did not receive adjuvant treatment, discontinuation of treatment prior to the adjuvant phase was due to an adverse event in 21 patients.

In the adjuvant phase, serious adverse reactions occurred in 43% of patients; the most frequent (≥2%) serious adverse reactions were urinary tract infection (8%), acute kidney injury and pyelonephritis (5% each), urosepsis (4%), and hypokalemia, intestinal obstruction, and sepsis (2% each). Fatal adverse reactions occurred in 7% of patients, including urosepsis, intracranial hemorrhage, death, myocardial infarction, multiple organ dysfunction syndrome, and pseudomonal pneumonia (1% each).

Permanent discontinuation of KEYTRUDA due to an adverse reaction occurred in 28% of patients. The most frequent (>1%) adverse reactions resulting in permanent discontinuation of KEYTRUDA were diarrhea (5%), and peripheral neuropathy, acute kidney injury, and pneumonitis (2% each).

Adverse reactions leading to dose interruption of KEYTRUDA in the adjuvant phase occurred in 38% of patients. The most common adverse reactions (≥2%) leading to dose interruption of KEYTRUDA were rash (7%), urinary tract infection (6%), diarrhea (4%), and abdominal pain, COVID-19, fatigue, pruritus, and pyelonephritis (2% each).

BCG-unresponsive High-risk NMIBC

The safety of KEYTRUDA was investigated in KEYNOTE-057, a multicenter, open-label, single-arm trial that enrolled 148 patients with high-risk non-muscle invasive bladder cancer (NMIBC), 96 of whom had BCG-unresponsive carcinoma in situ (CIS) with or without papillary tumors. Patients received KEYTRUDA 200 mg every 3 weeks until unacceptable toxicity, persistent or recurrent high-risk NMIBC or progressive disease, or up to 24 months of therapy without disease progression.

The median duration of exposure to KEYTRUDA was 4.3 months (range: 1 day to 25.6 months).

KEYTRUDA was discontinued due to adverse reactions in 11% of patients. The most common adverse (>1%) reaction resulting in permanent discontinuation of KEYTRUDA was pneumonitis (1.4%). Adverse reactions leading to interruption of KEYTRUDA occurred in 22% of patients; the most common (≥2%) were diarrhea (4%) and urinary tract infection (2%). Serious adverse reactions occurred in 28% of KEYTRUDA-treated patients. The most frequent serious adverse reactions (≥2%) in KEYTRUDA-treated patients were pneumonia (3%), cardiac ischemia (2%), colitis (2%), pulmonary embolism (2%), sepsis (2%), and urinary tract infection (2%). Tables 35 and 36 summarize adverse reactions and laboratory abnormalities, respectively, in patients on KEYTRUDA in KEYNOTE-057.

Table 35: Adverse Reactions Occurring in ≥10% of Patients Receiving KEYTRUDA in KEYNOTE-057
Adverse Reaction | KEYTRUDA 200 mg every 3 weeks N=148
Adverse Reaction | All Grades [Graded per NCI CTCAE v4.03] (%) | Grades 3–4 (%)
General
Fatigue [Includes asthenia, fatigue, malaise] | 29 | 0.7
Peripheral edema [Includes edema peripheral, peripheral swelling] | 11 | 0
Gastrointestinal
Diarrhea [Includes diarrhea, gastroenteritis, colitis] | 24 | 2.0
Nausea | 13 | 0
Constipation | 12 | 0
Skin and Subcutaneous Tissue
Rash [Includes rash maculo-papular, rash, rash erythematous, rash pruritic, rash pustular, erythema, eczema, eczema asteatotic, lichenoid keratosis, urticaria, dermatitis] | 24 | 0.7
Pruritus | 19 | 0.7
Musculoskeletal and Connective Tissue
Musculoskeletal pain [Includes back pain, myalgia, musculoskeletal pain, pain in extremity, musculoskeletal chest pain, neck pain] | 19 | 0
Arthralgia | 14 | 1.4
Renal and Urinary
Hematuria | 19 | 1.4
Respiratory, Thoracic, and Mediastinal
Cough [Includes cough, productive cough] | 19 | 0
Infections
Urinary tract infection | 12 | 2.0
Nasopharyngitis | 10 | 0
Endocrine
Hypothyroidism | 11 | 0

Table 36: Laboratory Abnormalities Worsened from Baseline Occurring in ≥20% of BCG-unresponsive NMIBC Patients Receiving KEYTRUDA in KEYNOTE-057
Laboratory Test [Each test incidence is based on the number of patients who had both baseline and at least one on-study laboratory measurement available: KEYTRUDA (range: 124 to 147 patients)] | KEYTRUDA 200 mg every 3 weeks
Laboratory Test [Each test incidence is based on the number of patients who had both baseline and at least one on-study laboratory measurement available: KEYTRUDA (range: 124 to 147 patients)] | All Grades [Graded per NCI CTCAE v4.03] (%) | Grades 3-4 (%)
Chemistry
Hyperglycemia | 59 | 7
Increased ALT | 25 | 2.7
Hyponatremia | 24 | 7
Hypophosphatemia | 24 | 6
Hypoalbuminemia | 24 | 1.4
Hyperkalemia | 23 | 1.4
Hypocalcemia | 22 | 0.7
Increased AST | 20 | 2.7
Increased creatinine | 20 | 0.7
Hematology
Anemia | 35 | 1.4
Lymphopenia | 29 | 1.6

Microsatellite Instability-High or Mismatch Repair Deficient Cancer

The safety of KEYTRUDA was investigated in 504 patients with MSI-H or dMMR cancer enrolled in KEYNOTE-158, KEYNOTE-164, and KEYNOTE-051 [see Clinical Studies (14.8)]. The median duration of exposure to KEYTRUDA was 6.2 months (range: 1 day to 53.5 months). Adverse reactions occurring in patients with MSI-H or dMMR cancer were similar to those occurring in patients with other solid tumors who received KEYTRUDA as a single agent.

Microsatellite Instability-High or Mismatch Repair Deficient Colorectal Cancer

Among the 153 patients with MSI-H or dMMR CRC enrolled in KEYNOTE-177 [see Clinical Studies (14.9)] treated with KEYTRUDA, the median duration of exposure to KEYTRUDA was 11.1 months (range: 1 day to 30.6 months). Patients with autoimmune disease or a medical condition that required immunosuppression were ineligible. Adverse reactions occurring in patients with MSI-H or dMMR CRC were similar to those occurring in 2799 patients with melanoma or NSCLC treated with KEYTRUDA as a single agent.

Gastric Cancer

First-line Treatment of Locally Advanced Unresectable or Metastatic HER2-Positive Gastric or Gastroesophageal Junction Adenocarcinoma

The safety of KEYTRUDA was evaluated in 696 patients with HER2-positive gastric or GEJ cancer enrolled in KEYNOTE-811, which included 350 patients treated with KEYTRUDA 200 mg, trastuzumab, and CAPOX (n=297) or FP (n=53) every 3 weeks, compared to 346 patients treated with placebo, trastuzumab, and CAPOX (n=298) or FP (n=48) every 3 weeks [see Clinical Studies (14.10)].

The median duration of exposure to KEYTRUDA was 9.2 months (range: 1 day to 33.6 months).

Fatal adverse reactions occurred in 3 patients who received KEYTRUDA in combination with trastuzumab and CAPOX or FP and included pneumonitis in 2 patients and hepatitis in 1 patient.

KEYTRUDA was discontinued due to adverse reactions in 13% of patients. Adverse reactions resulting in permanent discontinuation of KEYTRUDA in ≥1% of patients were pneumonitis (2.0%) and pneumonia (1.1%).

Adverse reactions leading to interruption of KEYTRUDA occurred in 71% of patients; the most common adverse reactions or laboratory abnormalities leading to interruption of KEYTRUDA (≥2%) were neutropenia (21%), thrombocytopenia (13%), diarrhea (7%), pneumonia (5%), anemia (4.9%), COVID-19 (3.1%), hypokalemia (3.1%), fatigue/asthenia (4.9%), decreased appetite (4%), increased AST (3.7%), increased blood bilirubin (4.6%), increased ALT (2.9%), vomiting (2.6%), pneumonitis (2.3%), pyrexia (2.3%), increased blood creatinine (2%), and colitis (2%).

In the KEYTRUDA arm versus placebo, there was a difference of ≥5% incidence between patients treated with KEYTRUDA versus standard of care for diarrhea (53% vs. 47%), rash (35% vs. 28%), hypothyroidism (11% vs. 5%), and pneumonia (11% vs. 5%). There were no clinically meaningful differences in incidence of Grade 3-4 toxicity between arms.

There was a difference of ≥5% incidence between patients treated with KEYTRUDA versus standard of care for decreased leukocytes (60% vs. 54%), decreased calcium (56% vs. 46%), decreased lymphocytes (59% vs. 51%), decreased potassium (41% vs. 36%), increased bilirubin (33% vs. 25%), increased creatinine (28% vs. 18%), and decreased glucose (17% vs. 11%). There were no clinically meaningful differences in incidence of Grade 3-4 toxicity between arms.

First-line Treatment of Locally Advanced Unresectable or Metastatic HER2-Negative Gastric or Gastroesophageal Junction Adenocarcinoma

The safety of KEYTRUDA was evaluated in 1572 patients with HER2-negative gastric or GEJ cancer enrolled in KEYNOTE-859, which included 785 patients treated with KEYTRUDA 200 mg and FP (n=106) or CAPOX (n=674) every 3 weeks, compared to 787 patients who received placebo and FP (n=107) or CAPOX (n=679) every 3 weeks [see Clinical Studies (14.10)].

The median duration of exposure to KEYTRUDA was 6.2 months (range: 1 day to 33.7 months).

Serious adverse reactions occurred in 45% of patients receiving KEYTRUDA. Serious adverse reactions in >2% of patients included pneumonia (4.1%), diarrhea (3.9%), hemorrhage (3.9%), and vomiting (2.4%). Fatal adverse reactions occurred in 8% of patients who received KEYTRUDA, including infection (2.3%) and thromboembolism (1.3%).

Permanent discontinuation of KEYTRUDA due to adverse reactions occurred in 15% of patients. Adverse reaction resulting in permanent discontinuation of KEYTRUDA in ≥1% were infections (1.8%) and diarrhea (1.0%).

Dosage interruptions of KEYTRUDA due to an adverse reaction occurred in 65% of patients. Adverse reactions or laboratory abnormalities leading to interruption of KEYTRUDA (≥2%) were neutropenia (21%), thrombocytopenia (13%), diarrhea (5.5%), fatigue (4.8%), infection (4.8%), anemia (4.5%), increased AST (4.3%), increased ALT (3.8%), increased blood bilirubin (3.3%), white blood cell count decreased (2.2%), nausea (2%), palmar-plantar erythrodysesthesia syndrome (2%), and vomiting (2%).

Tables 37 and 38 summarize adverse reactions and laboratory abnormalities, respectively, in patients on KEYTRUDA in KEYNOTE-859.

Table 37: Adverse Reactions Occurring in ≥20% of Patients Receiving KEYTRUDA in KEYNOTE-859
Adverse Reaction | KEYTRUDA 200 mg every 3 weeks and FP or CAPOX n=785 |  | Placebo and FP or CAPOX n=787
Adverse Reaction | All Grades [Graded per NCI CTCAE v4.03] (%) | Grades 3-4 (%) | All Grades (%) | Grades 3-4 (%)
Nervous System
Peripheral neuropathy [Includes dysesthesia, hyperesthesia, hypoesthesia, neuralgia, neuropathy peripheral, paresthesia, peripheral sensory neuropathy, peripheral motor neuropathy, polyneuropathy] | 47 | 5 | 48 | 6
Gastrointestinal
Nausea | 46 | 3.7 | 46 | 4.4
Diarrhea | 36 | 6 | 32 | 5
Vomiting | 34 | 5 | 27 | 5
Abdominal Pain [Includes abdominal discomfort, abdominal pain, abdominal pain lower, abdominal tenderness, abdominal pain upper, epigastric discomfort, gastrointestinal pain] | 26 | 2.8 | 24 | 2.9
Constipation | 22 | 0.5 | 21 | 0.8
General
Fatigue [Includes asthenia, fatigue] | 40 | 8 | 39 | 9
Metabolism and Nutrition
Decreased appetite | 29 | 3.3 | 29 | 2.5
Skin and Subcutaneous Tissue
Palmar-plantar erythrodysesthesia syndrome | 25 | 3.1 | 22 | 1.8
Investigations
Weight loss | 20 | 2.8 | 19 | 2.7

Table 38: Laboratory Abnormalities Worsened from Baseline Occurring in ≥20% of Patients Receiving KEYTRUDA in KEYNOTE-859
Laboratory Test [Each test incidence is based on the number of patients who had both baseline and at least one on-study laboratory measurement available: KEYTRUDA/FP or CAPOX (range: 210 to 766 patients) and placebo/FP or CAPOX (range: 190 to 762 patients)] | KEYTRUDA 200 mg every 3 weeks and FP or CAPOX |  | Placebo and FP or CAPOX
Laboratory Test [Each test incidence is based on the number of patients who had both baseline and at least one on-study laboratory measurement available: KEYTRUDA/FP or CAPOX (range: 210 to 766 patients) and placebo/FP or CAPOX (range: 190 to 762 patients)] | All Grades [Graded per NCI CTCAE v4.03] % | Grades 3-4 % | All Grades % | Grades 3-4 %
Hematology
Anemia | 65 | 15 | 69 | 13
Thrombocytopenia | 64 | 12 | 62 | 10
Neutropenia | 63 | 25 | 58 | 20
Leukopenia | 59 | 7 | 56 | 6
Lymphopenia | 57 | 20 | 51 | 16
Chemistry
Increased AST | 57 | 4.7 | 48 | 3.6
Hypoalbuminemia | 55 | 4.1 | 52 | 2.9
Hyperglycemia | 53 | 6 | 52 | 4.6
Hypocalcemia | 49 | 3.6 | 45 | 3.3
Increased alkaline phosphatase | 48 | 6 | 41 | 5
Hyponatremia | 40 | 13 | 40 | 12
Increased ALT | 40 | 4.2 | 29 | 2.9
Hypokalemia | 35 | 10 | 27 | 9
Bilirubin increased | 32 | 5 | 30 | 5
Hypophosphatemia | 30 | 10 | 27 | 8
Hypomagnesemia | 29 | 0.3 | 22 | 0.7
Increased creatinine | 21 | 3.5 | 18 | 1.7
Hyperkalemia | 20 | 3.7 | 18 | 2.9
Increased INR | 20 | 1.4 | 22 | 0

Esophageal Cancer

First-line Treatment of Locally Advanced Unresectable or Metastatic Esophageal Cancer/Gastroesophageal Junction

The safety of KEYTRUDA, in combination with cisplatin and FU chemotherapy was investigated in KEYNOTE-590, a multicenter, double-blind, randomized (1:1), placebo-controlled trial for the first-line treatment in patients with metastatic or locally advanced esophageal or gastroesophageal junction (tumors with epicenter 1 to 5 centimeters above the GEJ) carcinoma who were not candidates for surgical resection or definitive chemoradiation [see Clinical Studies (14.11)]. A total of 740 patients received either KEYTRUDA 200 mg (n=370) or placebo (n=370) every 3 weeks for up to 35 cycles, both in combination with up to 6 cycles of cisplatin and up to 35 cycles of FU.

The median duration of exposure was 5.7 months (range: 1 day to 26 months) in the KEYTRUDA combination arm and 5.1 months (range: 3 days to 27 months) in the chemotherapy arm.

KEYTRUDA was discontinued for adverse reactions in 15% of patients. The most common adverse reactions resulting in permanent discontinuation of KEYTRUDA (≥1%) were pneumonitis (1.6%), acute kidney injury (1.1%), and pneumonia (1.1%). Adverse reactions leading to interruption of KEYTRUDA occurred in 67% of patients. The most common adverse reactions leading to interruption of KEYTRUDA (≥2%) were neutropenia (19%), fatigue/asthenia (8%), decreased white blood cell count (5%), pneumonia (5%), decreased appetite (4.3%), anemia (3.2%), increased blood creatinine (3.2%), stomatitis (3.2%), malaise (3.0%), thrombocytopenia (3%), pneumonitis (2.7%), diarrhea (2.4%), dysphagia (2.2%), and nausea (2.2%).

Tables 39 and 40 summarize adverse reactions and laboratory abnormalities, respectively, in patients on KEYTRUDA in KEYNOTE-590.

Table 39: Adverse Reactions Occurring in ≥20% of Patients Receiving KEYTRUDA in KEYNOTE-590
Adverse Reaction | KEYTRUDA 200 mg every 3 weeks Cisplatin FU n=370 |  | Placebo Cisplatin FU n=370
Adverse Reaction | All Grades [Graded per NCI CTCAE v4.03] (%) | Grades 3-4 [One fatal event of diarrhea was reported in each arm.] (%) | All Grades (%) | Grades 3-4 (%)
Gastrointestinal
Nausea | 67 | 7 | 63 | 7
Constipation | 40 | 0 | 40 | 0
Diarrhea | 36 | 4.1 | 33 | 3
Vomiting | 34 | 7 | 32 | 5
Stomatitis | 27 | 6 | 26 | 3.8
General
Fatigue [Includes asthenia, fatigue] | 57 | 12 | 46 | 9
Metabolism and Nutrition
Decreased appetite | 44 | 4.1 | 38 | 5
Investigations
Weight loss | 24 | 3.0 | 24 | 5

Table 40: Laboratory Abnormalities Worsened from Baseline Occurring in ≥20% of Esophageal Cancer Patients Receiving KEYTRUDA in KEYNOTE-590
Laboratory Test [Each test incidence is based on the number of patients who had both baseline and at least one on-study laboratory measurement available: KEYTRUDA/cisplatin/FU (range: 353 to 365 patients) and placebo/cisplatin/FU (range: 347 to 359 patients)] | KEYTRUDA 200 mg every 3 weeks Cisplatin FU |  | Chemotherapy (Cisplatin and FU)
Laboratory Test [Each test incidence is based on the number of patients who had both baseline and at least one on-study laboratory measurement available: KEYTRUDA/cisplatin/FU (range: 353 to 365 patients) and placebo/cisplatin/FU (range: 347 to 359 patients)] | All Grades [Graded per NCI CTCAE v4.03] % | Grades 3-4 % | All Grades % | Grades 3-4 %
Hematology
Anemia | 84 | 21 | 87 | 25
Neutropenia | 77 | 44 | 73 | 41
Leukopenia | 73 | 21 | 73 | 17
Lymphopenia | 57 | 23 | 53 | 18
Thrombocytopenia | 43 | 5 | 46 | 8
Chemistry
Hyperglycemia | 56 | 7 | 55 | 6
Hyponatremia | 53 | 19 | 53 | 19
Hypoalbuminemia | 53 | 2.8 | 52 | 2.3
Increased creatinine | 45 | 2.5 | 42 | 2.5
Hypocalcemia | 44 | 3.9 | 37 | 2
Hypophosphatemia | 37 | 9 | 31 | 10
Hypokalemia | 30 | 12 | 34 | 15
Increased alkaline phosphatase | 29 | 1.9 | 29 | 1.7
Hyperkalemia | 28 | 3.6 | 28 | 2.5
Increased AST | 25 | 4.4 | 22 | 2.8
Increased ALT | 23 | 3.6 | 18 | 1.7

Previously Treated Recurrent Locally Advanced or Metastatic Esophageal Cancer

Among the 314 patients with esophageal cancer enrolled in KEYNOTE-181 [see Clinical Studies (14.11)] treated with KEYTRUDA, the median duration of exposure to KEYTRUDA was 2.1 months (range: 1 day to 24.4 months). Patients with autoimmune disease or a medical condition that required immunosuppression were ineligible. Adverse reactions occurring in patients with esophageal cancer were similar to those occurring in 2799 patients with melanoma or NSCLC treated with KEYTRUDA as a single agent.

Cervical Cancer

FIGO 2014 Stage III-IVA Cervical Cancer with Chemoradiotherapy

The safety of KEYTRUDA in combination with CRT (cisplatin plus external beam radiation therapy [EBRT] followed by brachytherapy [BT]) was investigated in KEYNOTE-A18, a placebo-controlled, randomized (1:1), multicenter, double-blind trial including 597 patients with FIGO 2014 Stage III-IVA cervical cancer [see Clinical Studies (14.12)]. Two hundred ninety-four patients received KEYTRUDA in combination with chemoradiotherapy and 303 patients received placebo in combination with chemoradiotherapy.

The median duration of exposure to KEYTRUDA was 20 months (range: 1 day to 32 months).

Fatal adverse reactions occurred in 1.4% of patients receiving KEYTRUDA in combination with chemoradiotherapy, including 1 case each (0.3%) of large intestinal perforation, urosepsis, sepsis, and vaginal hemorrhage.

Serious adverse reactions occurred in 34% of patients receiving KEYTRUDA in combination with chemoradiotherapy. Serious adverse reactions occurring in ≥1% of patients included urinary tract infection (3.1%), urosepsis (1.4%), and sepsis (1%).

KEYTRUDA was discontinued for adverse reactions in 9% of patients. The most common adverse reaction (≥1%) resulting in permanent discontinuation was diarrhea (1%).

Adverse reactions leading to interruption of KEYTRUDA occurred in 47% of patients; the most common adverse reactions leading to interruption of KEYTRUDA (≥2%) were anemia (7%), COVID-19 (7%), SARS-CoV-2 test positive (4.8%), diarrhea (4.1%), increased ALT (4.1%), increased AST (3.4%) decreased neutrophil count (3.1%), and urinary tract infection (2.7%).

Table 41 and Table 42 summarize adverse reactions and laboratory abnormalities, respectively, in patients on KEYTRUDA in KEYNOTE-A18.

Table 41: Adverse Reactions Occurring in ≥10% of Patients with FIGO 2014 Stage III-IVA Cervical Cancer Receiving KEYTRUDA in KEYNOTE-A18
Adverse Reaction | KEYTRUDA 200 mg every 3 weeks and 400 mg every 6 weeks with chemoradiotherapy n=294 |  | Placebo with chemoradiotherapy n=303
Adverse Reaction | All Grades [Graded per NCI CTCAE v5.0] (%) | Grades 3-4 (%) | All Grades (%) | Grades 3-4 (%)
Gastrointestinal
Nausea | 56 | 0 | 62 | 2.3
Diarrhea | 51 | 4.4 | 50 | 4.3
Vomiting | 34 | 1.0 | 35 | 1.7
Constipation | 20 | 0 | 19 | 0.7
Abdominal pain | 13 | 1.0 | 14 | 1.7
Infections
Urinary tract infection [Includes urinary tract infection, urinary tract infection pseudomonal, pyelonephritis acute, cystitis, Escherichia urinary tract infection] | 35 | 4.8 | 34 | 5
COVID-19 | 10 | 0 | 7 | 1.0
General
Fatigue [Includes fatigue, asthenia] | 28 | 1.0 | 28 | 1.3
Pyrexia | 14 | 0.7 | 15 | 0
Endocrine
Hypothyroidism [Includes hypothyroidism, autoimmune hypothyroidism] | 23 | 0.7 | 8 | 0
Hyperthyroidism | 13 | 0.3 | 3.3 | 0
Investigations
Weight loss | 19 | 2.4 | 19 | 1.0
Metabolism and Nutrition
Decreased appetite | 18 | 0.7 | 17 | 0.3
Renal and Urinary
Dysuria | 12 | 0.3 | 12 | 0
Skin and Subcutaneous Tissue Disorders
Rash [Includes erythema multiforme, dermatitis, drug eruption, eczema, rash, skin exfoliation, dermatitis bullous, rash maculo-papular, lichen planus, dyshidrotic eczema, dermatitis acneiform] | 12 | 1.0 | 8 | 0.3
Musculoskeletal and Connective Tissues Disorders
Back pain | 11 | 0.7 | 11 | 0.7
Reproductive System
Pelvic pain | 11 | 1.0 | 14 | 1.7

Table 42: Laboratory Abnormalities Worsened from Baseline Occurring in ≥20% of Patients with FIGO 2014 Stage III-IVA Cervical Cancer Receiving KEYTRUDA in KEYNOTE-A18
Laboratory Test [Laboratory abnormality percentage is based on the number of patients who had both baseline and at least one post-baseline laboratory measurement for each parameter: KEYTRUDA + chemoradiotherapy (range: 288 to 293 patients) and placebo + chemoradiotherapy (range: 299 to 301 patients)] | KEYTRUDA 200 mg every 3 weeks and 400 mg every 6 weeks with chemoradiotherapy |  | Placebo with chemoradiotherapy
Laboratory Test [Laboratory abnormality percentage is based on the number of patients who had both baseline and at least one post-baseline laboratory measurement for each parameter: KEYTRUDA + chemoradiotherapy (range: 288 to 293 patients) and placebo + chemoradiotherapy (range: 299 to 301 patients)] | All Grades [Graded per NCI CTCAE v5.0] (%) | Grades 3-4 (%) | All Grades (%) | Grades 3-4 (%)
Hematology
Lymphopenia | 99 | 96 | 99 | 92
Leukopenia | 96 | 48 | 94 | 49
Anemia | 87 | 33 | 82 | 27
Neutropenia | 76 | 33 | 76 | 33
Thrombocytopenia | 64 | 9 | 62 | 7
Chemistry
Hypomagnesemia | 61 | 4.2 | 63 | 3.7
Hyponatremia | 56 | 4.8 | 50 | 4.7
Increased AST | 50 | 1.7 | 44 | 2.3
Increased ALT | 49 | 3.1 | 46 | 1
Hypocalcemia | 45 | 5 | 43 | 5
Hypokalemia | 44 | 15 | 41 | 11
Increased creatinine | 44 | 7 | 46 | 6
Hypoalbuminemia | 38 | 2.4 | 37 | 2.3
Increased alkaline phosphatase | 38 | 0.3 | 35 | 0.3
Hyperkalemia | 21 | 2.0 | 16 | 1

Persistent, Recurrent, or Metastatic Cervical Cancer

The safety of KEYTRUDA in combination with paclitaxel and cisplatin or paclitaxel and carboplatin, with or without bevacizumab, was investigated in KEYNOTE-826, a multicenter, double-blind, randomized (1:1), placebo-controlled trial in patients with persistent, recurrent, or first-line metastatic cervical cancer who had not been treated with chemotherapy except when used concurrently as a radio-sensitizing agent [see Clinical Studies (14.12)]. A total of 616 patients, regardless of tumor PD-L1 expression, received KEYTRUDA 200 mg and chemotherapy with or without bevacizumab (n=307) every 3 weeks or placebo and chemotherapy with or without bevacizumab (n=309) every 3 weeks.

The median duration of exposure to KEYTRUDA was 9.9 months (range: 1 day to 26 months).

Fatal adverse reactions occurred in 4.6% of patients receiving KEYTRUDA in combination with chemotherapy with or without bevacizumab, including 3 cases of hemorrhage, 2 cases of sepsis, 2 cases due to unknown causes, and 1 case each of acute myocardial infarction, autoimmune encephalitis, cardiac arrest, cerebrovascular accident, femur fracture with perioperative pulmonary embolus, intestinal perforation, and pelvic infection.

Serious adverse reactions occurred in 50% of patients receiving KEYTRUDA in combination with chemotherapy with or without bevacizumab. Serious adverse reactions in ≥3% of patients included febrile neutropenia (6.8%), urinary tract infection (5.2%), anemia (4.6%), acute kidney injury (3.3%), and sepsis (3.3%).

KEYTRUDA was discontinued for adverse reactions in 15% of patients. The most common adverse reaction resulting in permanent discontinuation of KEYTRUDA (≥1%) was colitis (1%).

Adverse reactions leading to interruption of KEYTRUDA occurred in 66% of patients; the most common adverse reactions or laboratory abnormalities leading to interruption of KEYTRUDA (≥2%) were thrombocytopenia (15%), neutropenia (14%), anemia (11%), increased ALT (6%), leukopenia (5%), fatigue/asthenia (4.2%), urinary tract infection (3.6%), increased AST (3.3%), pyrexia (3.3%), diarrhea (2.6%), acute kidney injury (2.6%), increased blood creatinine (2.6%), colitis (2.3%), decreased appetite (2%), and cough (2%).

For patients treated with KEYTRUDA, chemotherapy, and bevacizumab (n=196), the most common (≥20%) adverse reactions were peripheral neuropathy (62%), alopecia (58%), anemia (55%), fatigue/asthenia (53%), nausea (41%), neutropenia (41%), diarrhea (39%), hypertension (35%), thrombocytopenia (35%), constipation (31%), arthralgia (31%), vomiting (30%), urinary tract infection (27%), rash (26%), leukopenia (24%), hypothyroidism (22%), and decreased appetite (21%).

Table 43 and Table 44 summarize adverse reactions and laboratory abnormalities, respectively, in patients on KEYTRUDA in KEYNOTE-826.

Table 43: Adverse Reactions Occurring in ≥20% of Patients Receiving KEYTRUDA in KEYNOTE-826
Adverse Reaction | KEYTRUDA 200 mg every 3 weeks and chemotherapy [Chemotherapy (paclitaxel and cisplatin or paclitaxel and carboplatin)] with or without bevacizumab n=307 |  | Placebo and chemotherapy with or without bevacizumab n=309
Adverse Reaction | All Grades [Graded per NCI CTCAE v4.0] (%) | Grades 3-4 (%) | All Grades (%) | Grades 3-4 (%)
Nervous System
Peripheral neuropathy [Includes neuropathy peripheral, peripheral sensory neuropathy, peripheral motor neuropathy, peripheral sensorimotor neuropathy, paresthesia] | 58 | 4.2 | 57 | 6
Skin and Subcutaneous Tissue
Alopecia | 56 | 0 | 58 | 0
Rash [Includes rash, rash maculo-papular, rash erythematous, rash macular, rash papular, rash pruritic, rash pustular] | 22 | 3.6 | 15 | 0.3
General
Fatigue [Includes fatigue, asthenia] | 47 | 7 | 46 | 6
Gastrointestinal
Nausea | 40 | 2 | 44 | 1.6
Diarrhea | 36 | 2 | 30 | 2.6
Constipation | 28 | 0.3 | 33 | 1
Vomiting | 26 | 2.6 | 27 | 1.9
Musculoskeletal and Connective Tissue
Arthralgia | 27 | 0.7 | 26 | 1.3
Vascular
Hypertension | 24 | 9 | 23 | 11
Infections
Urinary tract infection | 24 | 9 | 26 | 8

Table 44: Laboratory Abnormalities Worsened from Baseline Occurring in ≥20% of Patients Receiving KEYTRUDA in KEYNOTE-826
Laboratory Test [Each test incidence is based on the number of patients who had both baseline and at least one on-study laboratory measurement available: KEYTRUDA plus chemotherapy (range: 296 to 301 patients) and placebo plus chemotherapy (range: 299 to 302 patients)] | KEYTRUDA 200 mg every 3 weeks and chemotherapy [Chemotherapy (paclitaxel and cisplatin or paclitaxel and carboplatin)] with or without bevacizumab n=307 |  | Placebo and chemotherapy with or without bevacizumab n=309
Laboratory Test [Each test incidence is based on the number of patients who had both baseline and at least one on-study laboratory measurement available: KEYTRUDA plus chemotherapy (range: 296 to 301 patients) and placebo plus chemotherapy (range: 299 to 302 patients)] | All Grades [Graded per NCI CTCAE v4.0] (%) | Grades 3-4 (%) | All Grades (%) | Grades 3-4 (%)
Hematology
Anemia | 80 | 35 | 77 | 33
Leukopenia | 76 | 27 | 69 | 19
Neutropenia | 73 | 43 | 62 | 32
Lymphopenia | 64 | 35 | 59 | 35
Thrombocytopenia | 57 | 19 | 53 | 15
Chemistry
Hyperglycemia | 51 | 4.7 | 46 | 2.3
Hypoalbuminemia | 46 | 1.4 | 37 | 5
Hyponatremia | 39 | 14 | 38 | 11
Increased ALT | 40 | 7 | 38 | 6
Increased AST | 40 | 6 | 36 | 3.0
Increased alkaline phosphatase | 38 | 3.4 | 40 | 2.3
Hypocalcemia | 37 | 4.1 | 31 | 5
Increased creatinine | 34 | 5 | 32 | 6
Hypokalemia | 29 | 7 | 26 | 7
Hyperkalemia | 23 | 3.7 | 27 | 4.7
Hypercalcemia | 21 | 1.0 | 20 | 1.3

Previously Treated Recurrent or Metastatic Cervical Cancer

Among the 98 patients with cervical cancer enrolled in Cohort E of KEYNOTE-158 [see Clinical Studies (14.12)], the median duration of exposure to KEYTRUDA was 2.9 months (range: 1 day to 22.1 months). Patients with autoimmune disease or a medical condition that required immunosuppression were ineligible.

KEYTRUDA was discontinued due to adverse reactions in 8% of patients. Serious adverse reactions occurred in 39% of patients receiving KEYTRUDA. The most frequent serious adverse reactions reported included anemia (7%), fistula (4.1%), hemorrhage (4.1%), and infections [except UTIs] (4.1%). Tables 45 and 46 summarize adverse reactions and laboratory abnormalities, respectively, in patients on KEYTRUDA in KEYNOTE-158.

Table 45: Adverse Reactions Occurring in ≥10% of Patients with Cervical Cancer in KEYNOTE-158
Adverse Reaction | KEYTRUDA 200 mg every 3 weeks N=98
 | All Grades [Graded per NCI CTCAE v4.0] (%) | Grades 3–4 (%)
General
Fatigue [Includes asthenia, fatigue, lethargy, malaise] | 43 | 5
Pain [Includes breast pain, cancer pain, dysesthesia, dysuria, ear pain, gingival pain, groin pain, lymph node pain, oropharyngeal pain, pain, pain of skin, pelvic pain, radicular pain, stoma site pain, toothache] | 22 | 2.0
Pyrexia | 19 | 1.0
Edema peripheral [Includes edema peripheral, peripheral swelling] | 15 | 2.0
Musculoskeletal and Connective Tissue
Musculoskeletal pain [Includes arthralgia, back pain, musculoskeletal chest pain, musculoskeletal pain, myalgia, myositis, neck pain, non-cardiac chest pain, pain in extremity] | 27 | 5
Gastrointestinal
Diarrhea [Includes colitis, diarrhea, gastroenteritis] | 23 | 2.0
Abdominal pain [Includes abdominal discomfort, abdominal distension, abdominal pain, abdominal pain lower, abdominal pain upper] | 22 | 3.1
Nausea | 19 | 0
Vomiting | 19 | 1.0
Constipation | 14 | 0
Metabolism and Nutrition
Decreased appetite | 21 | 0
Vascular
Hemorrhage [Includes epistaxis, hematuria, hemoptysis, metrorrhagia, rectal hemorrhage, uterine hemorrhage, vaginal hemorrhage] | 19 | 5
Infections
UTI [Includes bacterial pyelonephritis, pyelonephritis acute, urinary tract infection, urinary tract infection bacterial, urinary tract infection pseudomonal, urosepsis] | 18 | 6
Infection (except UTI) [Includes cellulitis, clostridium difficile infection, device-related infection, empyema, erysipelas, herpes virus infection, infected neoplasm, infection, influenza, lower respiratory tract congestion, lung infection, oral candidiasis, oral fungal infection, osteomyelitis, pseudomonas infection, respiratory tract infection, tooth abscess, upper respiratory tract infection, uterine abscess, vulvovaginal candidiasis] | 16 | 4.1
Skin and Subcutaneous Tissue
Rash [Includes dermatitis, drug eruption, eczema, erythema, palmar-plantar erythrodysesthesia syndrome, rash, rash generalized, rash maculo-papular] | 17 | 2.0
Endocrine
Hypothyroidism | 11 | 0
Nervous System
Headache | 11 | 2.0
Respiratory, Thoracic and Mediastinal
Dyspnea | 10 | 1.0

Table 46: Laboratory Abnormalities Worsened from Baseline Occurring in ≥20% of Patients with Cervical Cancer in KEYNOTE-158
Laboratory Test [Each test incidence is based on the number of patients who had both baseline and at least one on-study laboratory measurement available: KEYTRUDA (range: 76 to 79 patients)] | KEYTRUDA 200 mg every 3 weeks
 | All Grades [Graded per NCI CTCAE v4.0] (%) | Grades 3-4 (%)
Hematology
Anemia | 54 | 24
Lymphopenia | 45 | 9
Chemistry
Hypoalbuminemia | 44 | 5
Increased alkaline phosphatase | 40 | 1.3
Hyponatremia | 38 | 13
Hyperglycemia | 38 | 1.3
Increased AST | 34 | 3.9
Increased creatinine | 32 | 5
Hypocalcemia | 27 | 0
Increased ALT | 21 | 3.9
Hypokalemia | 20 | 6

Other laboratory abnormalities occurring in ≥10% of patients receiving KEYTRUDA were hypophosphatemia (19% all Grades; 6% Grades 3-4), increased INR (17% all Grades; 0% Grades 3-4), hypercalcemia (14% all Grades; 2.6% Grades 3-4), platelet count decreased (14% all Grades; 1.3% Grades 3-4), activated partial thromboplastin time prolonged (10% all Grades; 0% Grades 3-4), hypoglycemia (13% all Grades; 1.3% Grades 3-4), white blood cell decreased (13% all Grades; 2.6% Grades 3-4), and hyperkalemia (13% all Grades; 1.3% Grades 3-4).

HCC

Previously Treated HCC

The safety of KEYTRUDA was investigated in KEYNOTE-394, a multicenter, double-blind, randomized, placebo-controlled trial that enrolled patients with previously treated HCC. Patients were randomized (2:1) and received KEYTRUDA 200 mg (n=299) or placebo (n=153) intravenously every 3 weeks for up to 35 cycles [see Clinical Studies (14.13)].

The median duration of exposure was 3.3 months (range: 1 day to 27.3 months) in the KEYTRUDA arm and 2.2 months (range: 1 day to 15.5 months) in the placebo arm. KEYTRUDA was discontinued due to adverse reactions in 13% of patients. The most common adverse reaction resulting in permanent discontinuation of KEYTRUDA was ascites (2.3%). Adverse reactions leading to interruption of KEYTRUDA occurred in 26% of patients; the most common adverse reactions or laboratory abnormalities leading to interruption of KEYTRUDA (≥2%) were increased blood bilirubin (9%), increased AST (5%), and increased ALT (2%).

Tables 47 and 48 summarize adverse reactions and laboratory abnormalities, respectively, in patients on KEYTRUDA in KEYNOTE-394.

Table 47: Adverse Reactions Occurring in ≥10% of Patients with HCC Receiving KEYTRUDA in KEYNOTE-394
Adverse Reaction | KEYTRUDA 200 mg every 3 weeks n=299 |  | Placebo n=153
Adverse Reaction | All Grades [Graded per NCI CTCAE v4.03] (%) | Grades 3-5 (%) | All Grades (%) | Grades 3-5 (%)
General
Pyrexia | 18 | 0.7 | 14 | 0
Skin and Subcutaneous Tissue
Rash [Includes dermatitis, dermatitis allergic, dermatitis bullous, rash, rash erythematous, rash maculo-papular, rash pustular, and blister.] | 18 | 0.7 | 7 | 0
Pruritus | 12 | 0 | 4 | 0
Gastrointestinal
Diarrhea | 16 | 1.7 | 9 | 0
Metabolism and Nutrition
Decreased appetite | 15 | 0.3 | 9 | 0
Infections
Upper respiratory tract infection | 11 | 1.0 | 7 | 0.7
Respiratory, Thoracic, and Mediastinal
Cough | 11 | 0 | 9 | 0
Endocrine
Hypothyroidism | 10 | 0 | 7 | 0

Table 48: Laboratory Abnormalities Worsened from Baseline Occurring in ≥20% of Patients with HCC Receiving KEYTRUDA in KEYNOTE-394
Laboratory Test [Each test incidence is based on the number of patients who had both baseline and at least one on-study laboratory measurement available: KEYTRUDA (range: 223 to 297 patients) and placebo (range: 144 to 151 patients).] | KEYTRUDA |  | Placebo
Laboratory Test [Each test incidence is based on the number of patients who had both baseline and at least one on-study laboratory measurement available: KEYTRUDA (range: 223 to 297 patients) and placebo (range: 144 to 151 patients).] | All Grades [Graded per NCI CTCAE v4.03] % | Grades 3-4 % | All Grades % | Grades 3-4 %
Chemistry
Increased AST | 54 | 14 | 44 | 12
Increased bilirubin | 47 | 11 | 36 | 7
Increased ALT | 47 | 7 | 32 | 4.6
Increased gamma-glutamyl transferase (GGT) | 40 | 20 | 39 | 15
Hypoalbuminemia | 40 | 0.7 | 20 | 0.7
Increased alkaline phosphatase | 39 | 4.1 | 34 | 4
Hyperglycemia | 36 | 3.3 | 26 | 1.4
Hyponatremia | 36 | 11 | 28 | 5
Hypophosphatemia | 30 | 6 | 17 | 4
Hypocalcemia | 24 | 1.4 | 15 | 0.7
Hematology
Lymphopenia | 44 | 11 | 34 | 4.6
Anemia | 36 | 7 | 30 | 3.3
Decreased platelets | 32 | 4.7 | 29 | 2
Leukopenia | 30 | 1.3 | 21 | 0.7
Neutropenia | 25 | 4.4 | 21 | 2

BTC

The safety of KEYTRUDA in combination with gemcitabine and cisplatin, was investigated in KEYNOTE-966, a multicenter, double-blind, randomized, placebo-controlled trial in patients with locally advanced unresectable or metastatic BTC who had not received prior systemic therapy in the advanced disease setting [see Clinical Studies (14.14)]. A total of 1063 patients received either KEYTRUDA 200 mg plus gemcitabine and cisplatin chemotherapy (n=529) or placebo plus gemcitabine and cisplatin chemotherapy (n=534) every 3 weeks.

The median duration of exposure to KEYTRUDA was 6 months (range: 1 day to 28 months).

KEYTRUDA was discontinued for adverse reactions in 15% of patients. The most common adverse reaction resulting in permanent discontinuation of KEYTRUDA (≥1%) was pneumonitis (1.3%).

Adverse reactions leading to the interruption of KEYTRUDA occurred in 55% of patients. The most common adverse reactions or laboratory abnormalities leading to interruption of KEYTRUDA (≥2%) were decreased neutrophil count (18%), decreased platelet count (10%), anemia (6%), decreased white blood count (4%), pyrexia (3.8%), fatigue (3.0%), cholangitis (2.8%), increased ALT (2.6%), increased AST (2.5%), and biliary obstruction (2.3%).

In the KEYTRUDA plus chemotherapy versus placebo plus chemotherapy arms, there was a difference of ≥5% incidence in adverse reactions between patients treated with KEYTRUDA versus placebo for pyrexia (26% vs. 20%), rash (21% vs. 13%), pruritus (15% vs. 10%), and hypothyroidism (9% vs. 2.6%). There were no clinically meaningful differences in incidence of Grade 3-4 toxicity between arms.

There was a difference of ≥5% incidence in laboratory abnormalities between patients treated with KEYTRUDA plus chemotherapy versus placebo plus chemotherapy for decreased lymphocytes (69% vs. 61%). There were no clinically meaningful differences in incidence of Grade 3-4 toxicity between arms.

MCC

Among the 105 patients with MCC enrolled in KEYNOTE-017 and KEYNOTE-913 [see Clinical Studies (14.15)], the median duration of exposure to KEYTRUDA was 6.3 months (range 1 day to 28 months). Patients with autoimmune disease or a medical condition that required immunosuppression were ineligible. Adverse reactions occurring in patients with MCC were similar to those occurring in 2799 patients with melanoma or NSCLC treated with KEYTRUDA as a single agent. Laboratory abnormalities (Grades 3-4) that occurred at a higher incidence included increased lipase (17%).

RCC

In combination with axitinib in the first-line treatment of advanced RCC (KEYNOTE-426)

The safety of KEYTRUDA in combination with axitinib was investigated in KEYNOTE-426 [see Clinical Studies (14.16)]. Patients with medical conditions that required systemic corticosteroids or other immunosuppressive medications or had a history of severe autoimmune disease other than type 1 diabetes, vitiligo, Sjogren's syndrome, and hypothyroidism stable on hormone replacement were ineligible. Patients received KEYTRUDA 200 mg intravenously every 3 weeks and axitinib 5 mg orally twice daily, or sunitinib 50 mg once daily for 4 weeks and then off treatment for 2 weeks. The median duration of exposure to the combination therapy of KEYTRUDA and axitinib was 10.4 months (range: 1 day to 21.2 months).

The study population characteristics were: median age of 62 years (range: 30 to 89), 40% age 65 or older; 71% male; 80% White; and 80% Karnofsky Performance Status (KPS) of 90-100 and 20% KPS of 70-80.

Fatal adverse reactions occurred in 3.3% of patients receiving KEYTRUDA in combination with axitinib. These included 3 cases of cardiac arrest, 2 cases of pulmonary embolism and 1 case each of cardiac failure, death due to unknown cause, myasthenia gravis, myocarditis, Fournier's gangrene, plasma cell myeloma, pleural effusion, pneumonitis, and respiratory failure.

Serious adverse reactions occurred in 40% of patients receiving KEYTRUDA in combination with axitinib. Serious adverse reactions in ≥1% of patients receiving KEYTRUDA in combination with axitinib included hepatotoxicity (7%), diarrhea (4.2%), acute kidney injury (2.3%), dehydration (1%), and pneumonitis (1%).

Permanent discontinuation due to an adverse reaction of either KEYTRUDA or axitinib occurred in 31% of patients; 13% KEYTRUDA only, 13% axitinib only, and 8% both drugs. The most common adverse reaction (>1%) resulting in permanent discontinuation of KEYTRUDA, axitinib, or the combination was hepatotoxicity (13%), diarrhea/colitis (1.9%), acute kidney injury (1.6%), and cerebrovascular accident (1.2%).

Dose interruptions or reductions due to an adverse reaction, excluding temporary interruptions of KEYTRUDA infusions due to infusion-related reactions, occurred in 76% of patients receiving KEYTRUDA in combination with axitinib. This includes interruption of KEYTRUDA in 50% of patients. Axitinib was interrupted in 64% of patients and dose reduced in 22% of patients. The most common adverse reactions (>10%) resulting in interruption of KEYTRUDA were hepatotoxicity (14%) and diarrhea (11%), and the most common adverse reactions (>10%) resulting in either interruption or reduction of axitinib were hepatotoxicity (21%), diarrhea (19%), and hypertension (18%).

The most common adverse reactions (≥20%) in patients receiving KEYTRUDA and axitinib were diarrhea, fatigue/asthenia, hypertension, hypothyroidism, decreased appetite, hepatotoxicity, palmar-plantar erythrodysesthesia, nausea, stomatitis/mucosal inflammation, dysphonia, rash, cough, and constipation.

Twenty-seven percent (27%) of patients treated with KEYTRUDA in combination with axitinib received an oral prednisone dose equivalent to ≥40 mg daily for an immune-mediated adverse reaction.

Tables 49 and 50 summarize the adverse reactions and laboratory abnormalities, respectively, that occurred in at least 20% of patients treated with KEYTRUDA and axitinib in KEYNOTE-426.

Table 49: Adverse Reactions Occurring in ≥20% of Patients Receiving KEYTRUDA with Axitinib in KEYNOTE-426
Adverse Reaction | KEYTRUDA 200 mg every 3 weeks and Axitinib n=429 |  | Sunitinib n=425
Adverse Reaction | All Grades [Graded per NCI CTCAE v4.03] (%) | Grades 3-4 (%) | All Grades (%) | Grades 3-4 (%)
Gastrointestinal
Diarrhea [Includes diarrhea, colitis, enterocolitis, gastroenteritis, enteritis, enterocolitis hemorrhagic] | 56 | 11 | 45 | 5
Nausea | 28 | 0.9 | 32 | 0.9
Constipation | 21 | 0 | 15 | 0.2
General
Fatigue/Asthenia | 52 | 5 | 51 | 10
Vascular
Hypertension [Includes hypertension, blood pressure increased, hypertensive crisis, labile hypertension] | 48 | 24 | 48 | 20
Hepatobiliary
Hepatotoxicity [Includes ALT increased, AST increased, autoimmune hepatitis, blood bilirubin increased, drug-induced liver injury, hepatic enzyme increased, hepatic function abnormal, hepatitis, hepatitis fulminant, hepatocellular injury, hepatotoxicity, hyperbilirubinemia, immune-mediated hepatitis, liver function test increased, liver injury, transaminases increased] | 39 | 20 | 25 | 4.9
Endocrine
Hypothyroidism | 35 | 0.2 | 32 | 0.2
Metabolism and Nutrition
Decreased appetite | 30 | 2.8 | 29 | 0.7
Skin and Subcutaneous Tissue
Palmar-plantar erythrodysesthesia syndrome | 28 | 5 | 40 | 3.8
Stomatitis/Mucosal inflammation | 27 | 1.6 | 41 | 4
Rash [Includes rash, butterfly rash, dermatitis, dermatitis acneform, dermatitis atopic, dermatitis bullous, dermatitis contact, exfoliative rash, genital rash, rash erythematous, rash generalized, rash macular, rash maculopapular, rash papular, rash pruritic, seborrheic dermatitis, skin discoloration, skin exfoliation, perineal rash] | 25 | 1.4 | 21 | 0.7
Respiratory, Thoracic and Mediastinal
Dysphonia | 25 | 0.2 | 3.3 | 0
Cough | 21 | 0.2 | 14 | 0.5

Table 50: Laboratory Abnormalities Worsened from Baseline Occurring in ≥20% of Patients Receiving KEYTRUDA with Axitinib in KEYNOTE-426
Laboratory Test [Each test incidence is based on the number of patients who had both baseline and at least one on-study laboratory measurement available: KEYTRUDA/axitinib (range: 342 to 425 patients) and sunitinib (range: 345 to 421 patients).] | KEYTRUDA 200 mg every 3 weeks and Axitinib |  | Sunitinib
Laboratory Test [Each test incidence is based on the number of patients who had both baseline and at least one on-study laboratory measurement available: KEYTRUDA/axitinib (range: 342 to 425 patients) and sunitinib (range: 345 to 421 patients).] | All Grades [Graded per NCI CTCAE v4.03] % | Grades 3-4 % | All Grades % | Grades 3-4 %
Chemistry
Hyperglycemia | 62 | 9 | 54 | 3.2
Increased ALT | 60 | 20 | 44 | 5
Increased AST | 57 | 13 | 56 | 5
Increased creatinine | 43 | 4.3 | 40 | 2.4
Hyponatremia | 35 | 8 | 29 | 8
Hyperkalemia | 34 | 6 | 22 | 1.7
Hypoalbuminemia | 32 | 0.5 | 34 | 1.7
Hypercalcemia | 27 | 0.7 | 15 | 1.9
Hypophosphatemia | 26 | 6 | 49 | 17
Increased alkaline phosphatase | 26 | 1.7 | 30 | 2.7
Hypocalcemia [Corrected for albumin] | 22 | 0.2 | 29 | 0.7
Blood bilirubin increased | 22 | 2.1 | 21 | 1.9
Activated partial thromboplastin time prolonged [Two patients with a Grade 3 elevated activated partial thromboplastin time prolonged (aPTT) were also reported as having an adverse reaction of hepatotoxicity.] | 22 | 1.2 | 14 | 0
Hematology
Lymphopenia | 33 | 11 | 47 | 9
Anemia | 29 | 2.1 | 65 | 8
Thrombocytopenia | 27 | 1.4 | 78 | 14

In combination with lenvatinib in the first-line treatment of advanced RCC (KEYNOTE-581)

The safety of KEYTRUDA was evaluated in KEYNOTE-581 [see Clinical Studies (14.16)]. Patients received KEYTRUDA 200 mg intravenously every 3 weeks in combination with lenvatinib 20 mg orally once daily (n=352), or lenvatinib 18 mg orally once daily in combination with everolimus 5 mg orally once daily (n=355), or sunitinib 50 mg orally once daily for 4 weeks then off treatment for 2 weeks (n=340). The median duration of exposure to the combination therapy of KEYTRUDA and lenvatinib was 17 months (range: 0.1 to 39).

Fatal adverse reactions occurred in 4.3% of patients treated with KEYTRUDA in combination with lenvatinib, including cardio-respiratory arrest (0.9%), sepsis (0.9%), and one case (0.3%) each of arrhythmia, autoimmune hepatitis, dyspnea, hypertensive crisis, increased blood creatinine, multiple organ dysfunction syndrome, myasthenic syndrome, myocarditis, nephritis, pneumonitis, ruptured aneurysm, and subarachnoid hemorrhage.

Serious adverse reactions occurred in 51% of patients receiving KEYTRUDA and lenvatinib. Serious adverse reactions in ≥2% of patients were hemorrhagic events (5%), diarrhea (4%), hypertension (3%), myocardial infarction (3%), pneumonitis (3%), vomiting (3%), acute kidney injury (2%), adrenal insufficiency (2%), dyspnea (2%), and pneumonia (2%).

Permanent discontinuation of either of KEYTRUDA, lenvatinib or both due to an adverse reaction occurred in 37% of patients receiving KEYTRUDA in combination with lenvatinib; 29% KEYTRUDA only, 26% lenvatinib only, and 13% both. The most common adverse reactions (≥2%) resulting in permanent discontinuation of KEYTRUDA, lenvatinib, or the combination were pneumonitis (3%), myocardial infarction (3%), hepatotoxicity (3%), acute kidney injury (3%), rash (3%), and diarrhea (2%).

Dose interruptions of KEYTRUDA, lenvatinib, or both due to an adverse reaction occurred in 78% of patients receiving KEYTRUDA in combination with lenvatinib. KEYTRUDA was interrupted in 55% of patients and both drugs were interrupted in 39% of patients. The most common adverse reactions (≥3%) resulting in interruption of KEYTRUDA were diarrhea (10%), hepatotoxicity (8%), fatigue (7%), lipase increased (5%), amylase increased (4%), musculoskeletal pain (3%), hypertension (3%), rash (3%), acute kidney injury (3%), and decreased appetite (3%).

Fifteen percent (15%) of patients treated with KEYTRUDA in combination with lenvatinib received an oral prednisone equivalent to ≥40 mg daily for an immune-mediated adverse reaction.

Tables 51 and 52 summarize the adverse reactions and laboratory abnormalities, respectively, that occurred in ≥20% of patients treated with KEYTRUDA and lenvatinib in KEYNOTE-581.

Table 51: Adverse Reactions Occurring in ≥20% of Patients Receiving KEYTRUDA with Lenvatinib in KEYNOTE-581
Adverse Reaction | KEYTRUDA 200 mg every 3 weeks with Lenvatinib N=352 |  | Sunitinib 50 mg N=340
Adverse Reaction | All Grades (%) | Grades 3-4 (%) | All Grades (%) | Grades 3-4 (%)
General
Fatigue [Includes asthenia, fatigue, lethargy, malaise] | 63 | 9 | 56 | 8
Gastrointestinal
Diarrhea [Includes diarrhea, gastroenteritis] | 62 | 10 | 50 | 6
Stomatitis [Includes aphthous ulcer, gingival pain, glossitis, glossodynia, mouth ulceration, mucosal inflammation, oral discomfort, oral mucosal blistering, oral pain, oropharyngeal pain, pharyngeal inflammation, stomatitis] | 43 | 2 | 43 | 2
Nausea | 36 | 3 | 33 | 1
Abdominal pain [Includes abdominal discomfort, abdominal pain, abdominal rigidity, abdominal tenderness, epigastric discomfort, lower abdominal pain, upper abdominal pain] | 27 | 2 | 18 | 1
Vomiting | 26 | 3 | 20 | 1
Constipation | 25 | 1 | 19 | 0
Musculoskeletal and Connective Tissue
Musculoskeletal disorders [Includes arthralgia, arthritis, back pain, bone pain, breast pain, musculoskeletal chest pain, musculoskeletal discomfort, musculoskeletal pain, musculoskeletal stiffness, myalgia, neck pain, non-cardiac chest pain, pain in extremity, pain in jaw] | 58 | 4 | 41 | 3
Endocrine
Hypothyroidism [Includes hypothyroidism, increased blood thyroid stimulating hormone, secondary hypothyroidism] | 57 | 1 | 32 | 0
Vascular
Hypertension [Includes essential hypertension, increased blood pressure, increased diastolic blood pressure, hypertension, hypertensive crisis, hypertensive retinopathy, labile blood pressure] | 56 | 29 | 43 | 20
Hemorrhagic events [Includes all hemorrhage terms. Hemorrhage terms that occurred in 1 or more subjects in either treatment group include Anal hemorrhage, aneurysm ruptured, blood blister, blood loss anemia, blood urine present, catheter site hematoma, cerebral microhemorrhage, conjunctival hemorrhage, contusion, diarrhea hemorrhagic, disseminated intravascular coagulation, ecchymosis, epistaxis, eye hemorrhage, gastric hemorrhage, gastritis hemorrhagic, gingival bleeding, hemorrhage urinary tract, hemothorax, hematemesis, hematoma, hematochezia, hematuria, hemoptysis, hemorrhoidal hemorrhage, increased tendency to bruise, injection site hematoma, injection site hemorrhage, intra-abdominal hemorrhage, lower gastrointestinal hemorrhage, Mallory-Weiss syndrome, melaena, petechiae, rectal hemorrhage, renal hemorrhage, retroperitoneal hemorrhage, small intestinal hemorrhage, splinter hemorrhages, subcutaneous hematoma, subdural hematoma, subarachnoid hemorrhage, thrombotic thrombocytopenic purpura, tumor hemorrhage, traumatic hematoma, upper gastrointestinal hemorrhage] | 27 | 5 | 26 | 4
Metabolism
Decreased appetite [Includes decreased appetite, early satiety] | 41 | 4 | 31 | 1
Skin and Subcutaneous Tissue
Rash [Includes genital rash, infusion site rash, penile rash, perineal rash, rash, rash erythematous, rash macular, rash maculo-papular, rash papular, rash pruritic, rash pustular] | 37 | 5 | 17 | 1
Palmar-plantar erythrodysesthesia syndrome [Includes palmar erythema, palmar-plantar erythrodysesthesia syndrome, plantar erythema] | 29 | 4 | 38 | 4
Investigations
Weight loss | 30 | 8 | 9 | 0.3
Respiratory, Thoracic and Mediastinal
Dysphonia | 30 | 0 | 4 | 0
Renal and Urinary
Proteinuria [Includes hemoglobinuria, nephrotic syndrome, proteinuria] | 30 | 8 | 13 | 3
Acute kidney injury [Includes acute kidney injury, azotemia, blood creatinine increased, creatinine renal clearance decreased, hypercreatininemia, renal failure, renal impairment, oliguria, glomerular filtration rate decreased, and nephropathy toxic] | 21 | 5 | 16 | 2
Hepatobiliary
Hepatotoxicity [Includes alanine aminotransferase increased, aspartate aminotransferase increased, blood bilirubin increased, drug-induced liver injury, hepatic enzyme increased, hepatic failure, hepatic function abnormal, hepatocellular injury, hepatotoxicity, hyperbilirubinemia, hypertransaminasemia, immune-mediated hepatitis, liver function test increased, liver injury, transaminases increased, gamma-glutamyltransferase increased] | 25 | 9 | 21 | 5
Nervous System
Headache | 23 | 1 | 16 | 1

Clinically relevant adverse reactions (<20%) that occurred in patients receiving KEYTRUDA with lenvatinib were myocardial infarction (3%) and angina pectoris (1%).

Table 52: Laboratory Abnormalities Worsened from Baseline Occurring in ≥20% (All Grades) of Patients Receiving KEYTRUDA with Lenvatinib in KEYNOTE-581
Laboratory Test [With at least one Grade increase from baseline] | KEYTRUDA 200 mg every 3 weeks with Lenvatinib |  | Sunitinib 50 mg
Laboratory Test [With at least one Grade increase from baseline] | All Grades % [Laboratory abnormality percentage is based on the number of patients who had both baseline and at least one post-baseline laboratory measurement for each parameter: KEYTRUDA with lenvatinib (range: 343 to 349 patients) and sunitinib (range: 329 to 335 patients).] | Grade 3-4 % | All Grades % | Grade 3-4 %
Chemistry
Hypertriglyceridemia | 80 | 15 | 71 | 15
Hypercholesterolemia | 64 | 5 | 43 | 1
Increased lipase | 61 | 34 | 59 | 28
Increased creatinine | 61 | 5 | 61 | 2
Increased amylase | 59 | 17 | 41 | 9
Increased AST | 58 | 7 | 57 | 3
Hyperglycemia | 55 | 7 | 48 | 3
Increased ALT | 52 | 7 | 49 | 4
Hyperkalemia | 44 | 9 | 28 | 6
Hypoglycemia | 44 | 2 | 27 | 1
Hyponatremia | 41 | 12 | 28 | 9
Decreased albumin | 34 | 0.3 | 22 | 0
Increased alkaline phosphatase | 32 | 4 | 32 | 1
Hypocalcemia | 30 | 2 | 22 | 1
Hypophosphatemia | 29 | 7 | 50 | 8
Hypomagnesemia | 25 | 2 | 15 | 3
Increased creatine phosphokinase | 24 | 6 | 36 | 5
Hypermagnesemia | 23 | 2 | 22 | 3
Hypercalcemia | 21 | 1 | 11 | 1
Hematology
Lymphopenia | 54 | 9 | 66 | 15
Thrombocytopenia | 39 | 2 | 73 | 13
Anemia | 38 | 3 | 66 | 8
Leukopenia | 34 | 1 | 77 | 8
Neutropenia | 31 | 4 | 72 | 16

Grade 3 and 4 increased ALT or AST was seen in 9% of patients. Grade ≥2 increased ALT or AST was reported in 64 (18%) patients, of whom 20 (31%) received ≥40 mg daily oral prednisone equivalent. Recurrence of Grade ≥2 increased ALT or AST was observed on rechallenge in 10 patients receiving both KEYTRUDA and lenvatinib (n=38) and was not observed on rechallenge with KEYTRUDA alone (n=3).

Adjuvant treatment of RCC

The safety of KEYTRUDA as a single agent was investigated in KEYNOTE-564, a randomized (1:1) double-blind placebo-controlled trial in which 984 patients who had undergone nephrectomy for RCC received 200 mg of KEYTRUDA by intravenous infusion every 3 weeks (n=488) or placebo (n=496) for up to one year [see Clinical Studies (14.16)]. The median duration of exposure to KEYTRUDA was 11.1 months (range: 1 day to 14.3 months). Patients with active autoimmune disease or a medical condition that required immunosuppression were ineligible.

Serious adverse reactions occurred in 20% of these patients receiving KEYTRUDA. Serious adverse reactions (≥1%) were acute kidney injury, adrenal insufficiency, pneumonia, colitis, and diabetic ketoacidosis (1% each). Fatal adverse reactions occurred in 0.2% of those treated with KEYTRUDA, including one case of pneumonia.

Discontinuation of KEYTRUDA due to an adverse reaction occurred in 21% of patients; the most common (≥1%) were increased ALT (1.6%), colitis (1%), and adrenal insufficiency (1%).

Dose interruptions of KEYTRUDA due to an adverse reaction occurred in 26% of patients; the most common (≥1%) were increased AST (2.3%), arthralgia (1.6%), hypothyroidism (1.6%), diarrhea (1.4%), increased ALT (1.4%), fatigue (1.4%), rash, decreased appetite, and vomiting (1% each). Tables 53 and 54 summarize adverse reactions and laboratory abnormalities, respectively, in patients on KEYTRUDA in KEYNOTE-564.

Table 53: Selected [Adverse reactions occurring at same or higher incidence than in placebo arm] Adverse Reactions Occurring in ≥10% of Patients Receiving KEYTRUDA in KEYNOTE-564
Adverse Reaction | KEYTRUDA 200 mg every 3 weeks n=488 |  | Placebo n=496
Adverse Reaction | All Grades [Graded per NCI CTCAE v4.0] (%) | Grades 3-4 (%) | All Grades (%) | Grades 3-4 (%)
Musculoskeletal and Connective Tissue
Musculoskeletal pain [Includes arthralgia, back pain, myalgia, arthritis, pain in extremity, neck pain, musculoskeletal pain, musculoskeletal stiffness, spinal pain, musculoskeletal chest pain, bone pain, musculoskeletal discomfort] | 41 | 1.2 | 36 | 0.6
General
Fatigue [Includes asthenia, fatigue] | 40 | 1.2 | 31 | 0.2
Skin and Subcutaneous Tissue
Rash [Includes rash, rash maculo-papular, rash papular, skin exfoliation, lichen planus, rash erythematous, eczema, rash macular, dermatitis acneiform, dermatitis, rash pruritic, Stevens-Johnson Syndrome, eczema asteatotic, palmar-plantar erythrodysesthesia syndrome] | 30 | 1.4 | 15 | 0.4
Pruritus | 23 | 0.2 | 13 | 0
Gastrointestinal
Diarrhea [Includes diarrhea, colitis, enterocolitis, frequent bowel movements, enteritis] | 27 | 2.7 | 23 | 0.2
Nausea | 16 | 0.4 | 10 | 0
Abdominal pain [Includes abdominal pain, abdominal pain lower, abdominal pain upper, abdominal discomfort, gastrointestinal pain] | 11 | 0.4 | 13 | 0.2
Endocrine
Hypothyroidism | 21 | 0.2 | 3.6 | 0
Hyperthyroidism | 12 | 0.2 | 0.2 | 0
Respiratory, Thoracic and Mediastinal
Cough [Includes upper-airway cough syndrome, productive cough, cough] | 17 | 0 | 12 | 0
Nervous System
Headache [Includes tension headache, headache, sinus headache, migraine with aura] | 15 | 0.2 | 13 | 0
Hepatobiliary
Hepatotoxicity [Includes alanine aminotransferase increased, aspartate aminotransferase increased, blood bilirubin increased, drug-induced liver injury, hepatic enzyme increased, hepatic function abnormal, hepatocellular injury, hepatotoxicity, hyperbilirubinemia, immune-mediated hepatitis, liver function test increased, transaminases increased, gamma-glutamyltransferase increased, bilirubin conjugated increased] | 14 | 3.7 | 7 | 0.6
Renal and Urinary
Acute kidney injury [Includes acute kidney injury, blood creatinine increased, renal failure, renal impairment, oliguria, glomerular filtration rate decreased, nephropathy toxic] | 13 | 1.2 | 10 | 0.2

Table 54: Selected [Laboratory abnormalities occurring at same or higher incidence than placebo] Laboratory Abnormalities Worsened from Baseline Occurring in ≥20% of Patients Receiving KEYTRUDA in KEYNOTE-564
Laboratory Test [Each test incidence is based on the number of patients who had both baseline and at least one on-study laboratory measurement available: KEYTRUDA (range: 440 to 449 patients) and placebo (range: 461 to 469 patients); increased INR: KEYTRUDA n=199 and placebo n=224.] | KEYTRUDA 200 mg every 3 weeks |  | Placebo
Laboratory Test [Each test incidence is based on the number of patients who had both baseline and at least one on-study laboratory measurement available: KEYTRUDA (range: 440 to 449 patients) and placebo (range: 461 to 469 patients); increased INR: KEYTRUDA n=199 and placebo n=224.] | All Grades [Graded per NCI CTCAE v4.03] % | Grades 3-4 % | All Grades % | Grades 3-4 %
Chemistry
Hyperglycemia | 48 | 8 | 45 | 4.5
Increased creatinine | 39 | 1.1 | 28 | 0.2
Increased INR | 29 | 1.0 | 20 | 0.9
Hyponatremia | 21 | 3.3 | 13 | 1.9
Increased ALT | 20 | 3.6 | 11 | 0.2
Hematology
Anemia | 28 | 0.5 | 20 | 0.4

Endometrial Carcinoma

Primary Advanced or Recurrent Endometrial Carcinoma

The safety of KEYTRUDA in combination with chemotherapy (paclitaxel and carboplatin) was investigated in KEYNOTE-868, a randomized (1:1), multicenter, double-blind, placebo-controlled trial that enrolled patients with advanced or recurrent endometrial carcinoma [see Clinical Studies (14.17)]. A total of 759 patients received KEYTRUDA 200 mg every 3 weeks and chemotherapy for 6 cycles followed by KEYTRUDA 400 mg every 6 weeks for up to 14 cycles (n=382) or placebo and chemotherapy for 6 cycles followed by placebo for up to 14 cycles (n=377). The median duration of exposure to KEYTRUDA was 5.6 months (range: 1 day to 24.0 months).

Serious adverse reactions occurred in 35% of patients receiving KEYTRUDA in combination with chemotherapy, compared to 19% of patients receiving placebo in combination with chemotherapy.

Fatal adverse reactions occurred in 1.6% of patients receiving KEYTRUDA in combination with chemotherapy, including COVID-19 (0.5%), and cardiac arrest (0.3%).

KEYTRUDA was discontinued for an adverse reaction in 14% of patients. Chemotherapy dose reduction was required in 29% of patients receiving KEYTRUDA in combination with chemotherapy, compared to 23% of patients receiving placebo in combination with chemotherapy. There were no clinically meaningful differences in chemotherapy discontinuations or interruptions between arms.

Adverse reactions occurring in patients treated with KEYTRUDA and chemotherapy were generally similar to those observed with KEYTRUDA alone or chemotherapy alone with the exception of rash (33% all Grades; 2.9% Grades 3-4).

In Combination with Lenvatinib for the Treatment of Advanced Endometrial Carcinoma That Is pMMR or Not MSI-H.

The safety of KEYTRUDA in combination with lenvatinib was investigated in KEYNOTE-775, a multicenter, open-label, randomized (1:1), active-controlled trial in patients with advanced endometrial carcinoma previously treated with at least one prior platinum-based chemotherapy regimen in any setting, including in the neoadjuvant and adjuvant settings [see Clinical Studies (14.17)]. Patients with endometrial carcinoma that is pMMR or not MSI-H received KEYTRUDA 200 mg every 3 weeks in combination with lenvatinib 20mg orally once daily (n=342) or received doxorubicin or paclitaxel (n=325).

For patients with pMMR or not MSI-H tumor status, the median duration of study treatment was 7.2 months (range 1 day to 26.8 months) and the median duration of exposure to KEYTRUDA was 6.8 months (range: 1 day to 25.8 months).

Fatal adverse reactions among these patients occurred in 4.7% of those treated with KEYTRUDA and lenvatinib, including 2 cases of pneumonia, and 1 case of the following: acute kidney injury, acute myocardial infarction, colitis, decreased appetite, intestinal perforation, lower gastrointestinal hemorrhage, malignant gastrointestinal obstruction, multiple organ dysfunction syndrome, myelodysplastic syndrome, pulmonary embolism, and right ventricular dysfunction.

Serious adverse reactions occurred in 50% of these patients receiving KEYTRUDA and lenvatinib. Serious adverse reactions (≥3%) were hypertension (4.4%) and urinary tract infections (3.2%).

Discontinuation of KEYTRUDA due to an adverse reaction occurred in 15% of these patients. The most common adverse reaction leading to discontinuation of KEYTRUDA (≥1%) was increased ALT (1.2%).

Dose interruptions of KEYTRUDA due to an adverse reaction occurred in 48% of these patients. The most common adverse reactions leading to interruption of KEYTRUDA (≥3%) were diarrhea (8%), increased ALT (4.4%), increased AST (3.8%), and hypertension (3.5%).

Tables 55 and 56 summarize adverse reactions and laboratory abnormalities, respectively, in patients on KEYTRUDA in combination with lenvatinib in KEYNOTE-775.

Table 55: Adverse Reactions Occurring in ≥20% of Patients with Endometrial Carcinoma in KEYNOTE-775
 | Endometrial Carcinoma (pMMR or not MSI-H)
Adverse Reaction | KEYTRUDA 200 mg every 3 weeks and Lenvatinib n=342 |  | Doxorubicin or Paclitaxel n=325
 | All Grades [Graded per NCI CTCAE v4.03] (%) | Grades 3-4 (%) | All Grades (%) | Grades 3-4 (%)
Endocrine
Hypothyroidism [Includes hypothyroidism, blood thyroid stimulating hormone increased, thyroiditis, secondary hypothyroidism] | 67 | 0.9 | 0.9 | 0
Vascular
Hypertension [Includes hypertension, blood pressure increased, secondary hypertension, blood pressure abnormal, hypertensive encephalopathy, blood pressure fluctuation] | 67 | 39 | 6 | 2.5
Hemorrhagic events [Includes epistaxis, vaginal hemorrhage, hematuria, gingival bleeding, metrorrhagia, rectal hemorrhage, contusion, hematochezia, cerebral hemorrhage, conjunctival hemorrhage, gastrointestinal hemorrhage, hemoptysis, hemorrhage urinary tract, lower gastrointestinal hemorrhage, mouth hemorrhage, petechiae, uterine hemorrhage, anal hemorrhage, blood blister, eye hemorrhage, hematoma, hemorrhage intracranial, hemorrhagic stroke, melena, stoma site hemorrhage, upper gastrointestinal hemorrhage, wound hemorrhage, blood urine present, ecchymosis, hematemesis, hemorrhage subcutaneous, hepatic hematoma, injection site bruising, intestinal hemorrhage, laryngeal hemorrhage, pulmonary hemorrhage, subdural hematoma, umbilical hemorrhage, vessel puncture site bruise] | 25 | 2.6 | 15 | 0.9
General
Fatigue [Includes fatigue, asthenia, malaise, lethargy] | 58 | 11 | 54 | 6
Gastrointestinal
Diarrhea [Includes diarrhea, gastroenteritis] | 55 | 8 | 20 | 2.8
Nausea | 49 | 2.9 | 47 | 1.5
Vomiting | 37 | 2.3 | 21 | 2.2
Stomatitis [Includes stomatitis, mucosal inflammation, oropharyngeal pain, aphthous ulcer, mouth ulceration, cheilitis, oral mucosal erythema, tongue ulceration] | 35 | 2.6 | 26 | 1.2
Abdominal pain [Includes abdominal pain, abdominal pain upper, abdominal pain lower, abdominal discomfort, gastrointestinal pain, abdominal tenderness, epigastric discomfort] | 34 | 2.6 | 21 | 1.2
Constipation | 27 | 0 | 25 | 0.6
Musculoskeletal and Connective Tissue
Musculoskeletal disorders [Includes arthralgia, myalgia, back pain, pain in extremity, bone pain, neck pain, musculoskeletal pain, arthritis, musculoskeletal chest pain, musculoskeletal stiffness, non-cardiac chest pain, pain in jaw] | 53 | 5 | 27 | 0.6
Metabolism
Decreased appetite [Includes decreased appetite, early satiety] | 44 | 7 | 21 | 0
Investigations
Weight loss | 34 | 10 | 6 | 0.3
Renal and Urinary
Proteinuria [Includes proteinuria, protein urine present, hemoglobinuria] | 29 | 6 | 3.4 | 0.3
Infections
Urinary tract infection [Includes urinary tract infection, cystitis, pyelonephritis] | 31 | 5 | 13 | 1.2
Nervous System
Headache | 26 | 0.6 | 9 | 0.3
Respiratory, Thoracic and Mediastinal
Dysphonia | 22 | 0 | 0.6 | 0
Skin and Subcutaneous Tissue
Palmar-plantar erythrodysesthesia [Includes palmar-plantar erythrodysesthesia syndrome, palmar erythema, plantar erythema] | 23 | 2.9 | 0.9 | 0
Rash [Includes rash, rash maculo-papular, rash pruritic, rash erythematous, rash macular, rash pustular, rash papular, rash vesicular, application site rash] | 20 | 2.3 | 4.9 | 0

Table 56: Laboratory Abnormalities Worsened from Baseline [With at least one grade increase from baseline] Occurring in ≥20% (All Grades) or ≥3% (Grades 3-4) of Patients with Endometrial Carcinoma in KEYNOTE-775
 | Endometrial Carcinoma (pMMR or not MSI-H)
Laboratory Test [Laboratory abnormality percentage is based on the number of patients who had both baseline and at least one post-baseline laboratory measurement for each parameter: KEYTRUDA and lenvatinib (range: 263 to 340 patients) and doxorubicin or paclitaxel (range: 240 to 322 patients).] | KEYTRUDA 200 mg every 3 weeks and Lenvatinib |  | Doxorubicin or Paclitaxel
 | All Grades [Graded per NCI CTCAE v4.03] % | Grades 3-4 % | All Grades % | Grades 3-4 %
Chemistry
Hypertriglyceridemia | 70 | 6 | 45 | 1.7
Hypoalbuminemia | 60 | 2.7 | 42 | 1.6
Increased aspartate aminotransferase | 58 | 9 | 23 | 1.6
Hyperglycemia | 58 | 8 | 45 | 4.4
Hypomagnesemia | 46 | 0 | 27 | 1.3
Increased alanine aminotransferase | 55 | 9 | 21 | 1.2
Hypercholesterolemia | 53 | 3.2 | 23 | 0.7
Hyponatremia | 46 | 15 | 28 | 7
Increased alkaline phosphatase | 43 | 4.7 | 18 | 0.9
Hypocalcemia | 40 | 4.7 | 21 | 1.9
Increased lipase | 36 | 14 | 13 | 3.9
Increased creatinine | 35 | 4.7 | 18 | 1.9
Hypokalemia | 34 | 10 | 24 | 5
Hypophosphatemia | 26 | 8 | 17 | 3.2
Increased amylase | 25 | 7 | 8 | 1
Hyperkalemia | 23 | 2.4 | 12 | 1.2
Increased creatine kinase | 19 | 3.7 | 7 | 0
Increased bilirubin | 18 | 3.6 | 6 | 1.6
Hematology
Lymphopenia | 51 | 18 | 66 | 23
Thrombocytopenia | 50 | 8 | 30 | 4.7
Anemia | 49 | 8 | 84 | 14
Leukopenia | 43 | 3.5 | 83 | 43
Neutropenia | 34 | 8 | 80 | 60

As a Single Agent for the Treatment of Advanced MSI-H or dMMR Endometrial Carcinoma

Among the 90 patients with MSI-H or dMMR endometrial carcinoma enrolled in KEYNOTE-158 [see Clinical Studies (14.17)] treated with KEYTRUDA as a single agent, the median duration of exposure to KEYTRUDA was 8.3 months (range: 1 day to 26.9 months). Adverse reactions occurring in patients with endometrial carcinoma were similar to those occurring in 2799 patients with melanoma or NSCLC treated with KEYTRUDA as a single agent.

TMB-H Cancer

The safety of KEYTRUDA was investigated in 105 patients with TMB-H cancer enrolled in KEYNOTE-158 [see Clinical Studies (14.18)]. The median duration of exposure to KEYTRUDA was 4.9 months (range: 0.03 to 35.2 months). Adverse reactions occurring in patients with TMB-H cancer were similar to those occurring in patients with other solid tumors who received KEYTRUDA as a single agent.

cSCC

Among the 159 patients with advanced cSCC (recurrent or metastatic or locally advanced disease) enrolled in KEYNOTE-629 [see Clinical Studies (14.19)], the median duration of exposure to KEYTRUDA was 6.9 months (range 1 day to 28.9 months). Patients with autoimmune disease or a medical condition that required systemic corticosteroids or other immunosuppressive medications were ineligible. Adverse reactions occurring in patients with recurrent or metastatic cSCC or locally advanced cSCC were similar to those occurring in 2799 patients with melanoma or NSCLC treated with KEYTRUDA as a single agent. Laboratory abnormalities (Grades 3-4) that occurred at a higher incidence included lymphopenia (10%) and decreased sodium (10%).

TNBC

Neoadjuvant and Adjuvant Treatment of High-Risk Early-Stage TNBC

The safety of KEYTRUDA in combination with neoadjuvant chemotherapy (carboplatin and paclitaxel followed by doxorubicin or epirubicin and cyclophosphamide) followed by surgery and continued adjuvant treatment with KEYTRUDA as a single agent was investigated in KEYNOTE-522, a randomized (2:1), multicenter, double-blind, placebo-controlled trial in patients with newly diagnosed, previously untreated, high-risk early-stage TNBC.

A total of 778 patients on the KEYTRUDA arm received at least 1 dose of KEYTRUDA in combination with neoadjuvant chemotherapy followed by KEYTRUDA as adjuvant treatment after surgery, compared to 389 patients who received at least 1 dose of placebo in combination with neoadjuvant chemotherapy followed by placebo as adjuvant treatment after surgery [see Clinical Studies (14.20)].

The median duration of exposure to KEYTRUDA 200 mg every 3 weeks was 13.3 months (range: 1 day to 21.9 months).

Fatal adverse reactions occurred in 0.9% of patients receiving KEYTRUDA, including 1 each of adrenal crisis, autoimmune encephalitis, hepatitis, pneumonia, pneumonitis, pulmonary embolism, and sepsis in association with multiple organ dysfunction syndrome and myocardial infarction.

Serious adverse reactions occurred in 44% of patients receiving KEYTRUDA. Serious adverse reactions in ≥2% of patients who received KEYTRUDA included febrile neutropenia (15%), pyrexia (3.7%), anemia (2.6%), and neutropenia (2.2%).

KEYTRUDA was discontinued for adverse reactions in 20% of patients. The most common adverse reactions (≥1%) resulting in permanent discontinuation of KEYTRUDA were increased ALT (2.7%), increased AST (1.5%), and rash (1%). Adverse reactions leading to the interruption of KEYTRUDA occurred in 57% of patients. The most common adverse reactions leading to interruption of KEYTRUDA (≥2%) were neutropenia (26%), thrombocytopenia (6%), increased ALT (6%), increased AST (3.7%), anemia (3.5%), rash (3.2%), febrile neutropenia (2.8%), leukopenia (2.8%), upper respiratory tract infection (2.6%), pyrexia (2.2%), and fatigue (2.1%).

Tables 57 and 58 summarize the adverse reactions and laboratory abnormalities, respectively, in patients treated with KEYTRUDA in KEYNOTE-522.

Table 57: Adverse Reactions Occurring in ≥20% of Patients Receiving KEYTRUDA in KEYNOTE-522
Adverse Reaction | KEYTRUDA 200 mg every 3 weeks with chemotherapy [Chemotherapy: carboplatin and paclitaxel followed by doxorubicin or epirubicin and cyclophosphamide] /KEYTRUDA n=778 |  | Placebo with chemotherapy/Placebo n=389
Adverse Reaction | All Grades [Graded per NCI CTCAE v4.0] (%) | Grades 3-4 (%) | All Grades (%) | Grades 3-4 (%)
General
Fatigue [Includes asthenia, fatigue] | 70 | 8 | 66 | 3.9
Pyrexia | 28 | 1.3 | 19 | 0.3
Gastrointestinal
Nausea | 67 | 3.7 | 66 | 1.8
Constipation | 42 | 0 | 39 | 0.3
Diarrhea | 41 | 3.2 | 34 | 1.8
Stomatitis [Includes aphthous ulcer, cheilitis, lip pain, lip ulceration, mouth ulceration, mucosal inflammation, oral mucosal eruption, oral pain, stomatitis, tongue blistering, tongue ulceration] | 34 | 2.7 | 29 | 1
Vomiting | 31 | 2.7 | 28 | 1.5
Abdominal pain [Includes abdominal discomfort, abdominal pain, abdominal pain lower, abdominal pain upper, abdominal tenderness] | 24 | 0.5 | 23 | 0.8
Skin and Subcutaneous Tissue
Alopecia | 61 | 0 | 58 | 0
Rash [Includes dermatitis, dermatitis acneiform, dermatitis allergic, dermatitis bullous, dermatitis exfoliative generalized, drug eruption, eczema, incision site rash, injection site rash, rash, rash erythematous, rash follicular, rash macular, rash maculo-papular, rash morbilliform, rash papular, rash pruritic, rash pustular, rash rubelliform, skin exfoliation, skin toxicity, toxic skin eruption, urticaria, vasculitic rash, viral rash] | 52 | 5 | 41 | 0.5
Nervous System
Peripheral neuropathy [Includes neuropathy peripheral, peripheral motor neuropathy, peripheral sensorimotor neuropathy, peripheral sensory neuropathy] | 41 | 3.3 | 42 | 2.3
Headache | 30 | 0.5 | 29 | 1
Musculoskeletal and Connective Tissue
Arthralgia | 29 | 0.5 | 31 | 0.3
Myalgia | 20 | 0.5 | 19 | 0
Respiratory, Thoracic and Mediastinal
Cough [Includes cough, productive cough, upper-airway cough syndrome] | 26 | 0.1 | 24 | 0
Metabolism and Nutrition
Decreased appetite | 23 | 0.9 | 17 | 0.3
Psychiatric
Insomnia | 21 | 0.5 | 19 | 0

Table 58: Laboratory Abnormalities Worsened from Baseline Occurring in ≥20% of Patients Receiving KEYTRUDA in KEYNOTE-522
Laboratory Test [Each test incidence is based on the number of patients who had both baseline and at least one on-study laboratory measurement available: KEYTRUDA in combination with chemotherapy followed by KEYTRUDA as a single agent (range: 762 to 777 patients) and placebo in combination with chemotherapy followed by placebo (range: 381 to 389 patients).] | KEYTRUDA 200 mg every 3 weeks with chemotherapy [Chemotherapy: carboplatin and paclitaxel followed by doxorubicin or epirubicin and cyclophosphamide] /KEYTRUDA |  | Placebo with chemotherapy/Placebo
Laboratory Test [Each test incidence is based on the number of patients who had both baseline and at least one on-study laboratory measurement available: KEYTRUDA in combination with chemotherapy followed by KEYTRUDA as a single agent (range: 762 to 777 patients) and placebo in combination with chemotherapy followed by placebo (range: 381 to 389 patients).] | All Grades [Graded per NCI CTCAE v4.0] % | Grades 3-4 % | All Grades % | Grades 3-4 %
Hematology
Anemia | 97 | 22 | 96 | 19
Leukopenia | 93 | 41 | 91 | 32
Neutropenia | 88 | 62 | 89 | 62
Lymphopenia | 79 | 28 | 74 | 22
Thrombocytopenia | 57 | 10 | 56 | 8
Chemistry
Increased ALT | 70 | 9 | 67 | 3.9
Increased AST | 65 | 6 | 56 | 1.5
Hyperglycemia | 63 | 4.3 | 61 | 2.8
Increased alkaline phosphatase | 37 | 1 | 35 | 0.5
Hyponatremia | 35 | 9 | 25 | 4.6
Hypoalbuminemia | 34 | 1.0 | 30 | 1.3
Hypocalcemia | 31 | 2.2 | 28 | 3.1
Hypokalemia | 31 | 6 | 22 | 2.8
Hypophosphatemia | 20 | 6 | 15 | 4.2

Locally Recurrent Unresectable or Metastatic TNBC

The safety of KEYTRUDA in combination with paclitaxel, paclitaxel protein-bound, or gemcitabine and carboplatin was investigated in KEYNOTE-355, a multicenter, double-blind, randomized (2:1), placebo-controlled trial in patients with locally recurrent unresectable or metastatic TNBC who had not been previously treated with chemotherapy in the metastatic setting [see Clinical Studies (14.20)]. A total of 596 patients (including 34 patients from a safety run-in) received KEYTRUDA 200 mg every 3 weeks in combination with paclitaxel, paclitaxel protein-bound, or gemcitabine and carboplatin.

The median duration of exposure to KEYTRUDA was 5.7 months (range: 1 day to 33.0 months).

Fatal adverse reactions occurred in 2.5% of patients receiving KEYTRUDA in combination with chemotherapy, including cardio-respiratory arrest (0.7%) and septic shock (0.3%).

Serious adverse reactions occurred in 30% of patients receiving KEYTRUDA in combination with paclitaxel, paclitaxel protein-bound, or gemcitabine and carboplatin. Serious adverse reactions in ≥2% of patients were pneumonia (2.9%), anemia (2.2%), and thrombocytopenia (2%).

KEYTRUDA was discontinued for adverse reactions in 11% of patients. The most common adverse reactions resulting in permanent discontinuation of KEYTRUDA (≥1%) were increased ALT (2.2%), increased AST (1.5%), and pneumonitis (1.2%). Adverse reactions leading to the interruption of KEYTRUDA occurred in 50% of patients. The most common adverse reactions leading to interruption of KEYTRUDA (≥2%) were neutropenia (22%), thrombocytopenia (14%), anemia (7%), increased ALT (6%), leukopenia (5%), increased AST (5%), decreased white blood cell count (3.9%), and diarrhea (2%).

Tables 59 and 60 summarize the adverse reactions and laboratory abnormalities in patients on KEYTRUDA in KEYNOTE-355.

Table 59: Adverse Reactions Occurring in ≥20% of Patients Receiving KEYTRUDA with Chemotherapy in KEYNOTE-355
Adverse Reaction | KEYTRUDA 200 mg every 3 weeks with chemotherapy n=596 |  | Placebo every 3 weeks with chemotherapy n=281
Adverse Reaction | All Grades [Graded per NCI CTCAE v4.03] (%) | Grades 3-4 (%) | All Grades (%) | Grades 3-4 (%)
General
Fatigue [Includes fatigue and asthenia] | 48 | 5 | 49 | 4.3
Gastrointestinal
Nausea | 44 | 1.7 | 47 | 1.8
Diarrhea | 28 | 1.8 | 23 | 1.8
Constipation | 28 | 0.5 | 27 | 0.4
Vomiting | 26 | 2.7 | 22 | 3.2
Skin and Subcutaneous Tissue
Alopecia | 34 | 0.8 | 35 | 1.1
Rash [Includes rash, rash maculo-papular, rash pruritic, rash pustular, rash macular, rash papular, butterfly rash, rash erythematous, eyelid rash] | 26 | 2 | 16 | 0
Respiratory, Thoracic and Mediastinal
Cough [Includes cough, productive cough, upper-airway cough syndrome] | 23 | 0 | 20 | 0.4
Metabolism and Nutrition
Decreased appetite | 21 | 0.8 | 14 | 0.4
Nervous System
Headache [Includes headache, migraine, tension headache] | 20 | 0.7 | 23 | 0.7

Table 60: Laboratory Abnormalities Worsened from Baseline Occurring in ≥20% of Patients Receiving KEYTRUDA with Chemotherapy in KEYNOTE-355
Laboratory Test [Each test incidence is based on the number of patients who had both baseline and at least one on-study laboratory measurement available: KEYTRUDA + chemotherapy (range: 566 to 592 patients) and placebo + chemotherapy (range: 269 to 280 patients).] | KEYTRUDA 200 mg every 3 weeks with chemotherapy |  | Placebo every 3 weeks with chemotherapy
Laboratory Test [Each test incidence is based on the number of patients who had both baseline and at least one on-study laboratory measurement available: KEYTRUDA + chemotherapy (range: 566 to 592 patients) and placebo + chemotherapy (range: 269 to 280 patients).] | All Grades [Graded per NCI CTCAE v4.03] % | Grades 3-4 % | All Grades % | Grades 3-4 %
Hematology
Anemia | 90 | 20 | 85 | 19
Leukopenia | 85 | 39 | 86 | 39
Neutropenia | 78 | 50 | 79 | 53
Lymphopenia | 73 | 28 | 71 | 19
Thrombocytopenia | 54 | 19 | 53 | 21
Chemistry
Increased ALT | 60 | 11 | 58 | 8
Increased AST | 57 | 9 | 55 | 6
Hyperglycemia | 52 | 4.4 | 51 | 2.2
Hypoalbuminemia | 36 | 2.0 | 32 | 2.2
Increased alkaline phosphatase | 35 | 3.9 | 39 | 2.2
Hypocalcemia | 29 | 3.3 | 27 | 1.8
Hyponatremia | 28 | 5 | 26 | 6
Hypophosphatemia | 21 | 7 | 18 | 4.8
Hypokalemia | 20 | 4.4 | 18 | 4.0

Ovarian Cancer

The safety of KEYTRUDA in combination with paclitaxel with or without bevacizumab was evaluated in 463 patients with epithelial ovarian, fallopian tube, or primary peritoneal carcinoma whose tumors express PD-L1 (CPS ≥1) enrolled in KEYNOTE-B96 [see Clinical Studies (14.21)]. Among patients who received KEYTRUDA, the median duration of exposure was 7.4 months (range: 1 day to 35.9 months).

Serious adverse reactions occurred in 54% of patients receiving KEYTRUDA and paclitaxel with or without bevacizumab. Serious adverse reactions in ≥2% of patients were pneumonia (4.3%), urinary tract infection (3.9%), adrenal insufficiency (3%), hyponatremia (3%), COVID-19 (2.6%), decreased neutrophil count (2.6%), pulmonary embolism (2.6%), abdominal pain (2.1%), anemia (2.1%), colitis (2.1%), diarrhea (2.1%), febrile neutropenia (2.1%), pyrexia (2.1%) and vomiting (2.1%).

Fatal adverse reactions occurred in 3.9% of patients receiving KEYTRUDA and paclitaxel with or without bevacizumab, including assisted suicide (0.9%), death (0.4%), intestinal perforation (0.4%), sepsis (0.4%), COVID-19 (0.4%), cardio-respiratory arrest (0.4%), colitis (0.4%), and embolic stroke (0.4%).

KEYTRUDA was permanently discontinued for adverse reactions in 16% of patients. The most common adverse reactions resulting in permanent discontinuation of KEYTRUDA (≥1%) were colitis (1.3%), and increased alanine aminotransferase (1.3%). Adverse reactions leading to the interruption of KEYTRUDA occurred in 44% of patients. The most common adverse reactions leading to interruption of KEYTRUDA in ≥2% were urinary tract infection (3.9%), adrenal insufficiency (2.6%), pyrexia (2.6%), pneumonitis (2.6%), upper respiratory tract infection (2.6%), neutropenia (2.1%), diarrhea (2.1%) and COVID-19 (2.1%).

The most common (≥20%) adverse reactions for patients treated with KEYTRUDA in combination with paclitaxel with or without bevacizumab were: diarrhea (45%), fatigue (43%), nausea (41%), alopecia (38%), peripheral neuropathy (38%), epistaxis (31%), urinary tract infection (27%), constipation (25%), abdominal pain (24%), decreased appetite (24%), vomiting (24%), hypothyroidism (21%), cough (20%), hypertension (20%), and rash (20%). The most common (≥20%) laboratory abnormalities worsening from baseline were: anemia (85%), leukopenia (82%), decreased neutrophil count (71%), lymphopenia (60%), hypoalbuminemia (50%), hyponatremia (53%), hypomagnesemia (45%), increased aspartate aminotransferase (43%), increased alanine aminotransferase (40%), hypocalcemia (40%), increased alkaline phosphatase (31%), increased creatinine (29%), hypokalemia (27%) and neutropenia (21%).

For patients treated with KEYTRUDA in combination with paclitaxel and bevacizumab (N=169), decreased white blood cell count (27%), stomatitis (22%) and pyrexia (21%) were also reported as adverse reactions.

6.2 Postmarketing Experience

The following adverse reactions have been identified during postapproval use of KEYTRUDA. Because these reactions are reported voluntarily from a population of uncertain size, it is not always possible to reliably estimate their frequency or establish a causal relationship to drug exposure.

Gastrointestinal: Exocrine pancreatic insufficiency

Hepatobiliary: sclerosing cholangitis

8 USE IN SPECIFIC POPULATIONS

8.1 Pregnancy

Risk Summary

Based on its mechanism of action, KEYTRUDA can cause fetal harm when administered to a pregnant woman. There are no available human data informing the risk of embryo-fetal toxicity. In animal models, the PD-1/PD-L1 signaling pathway is important in the maintenance of pregnancy through induction of maternal immune tolerance to fetal tissue (see Data). Human IgG4 (immunoglobulins) are known to cross the placenta; therefore, pembrolizumab has the potential to be transmitted from the mother to the developing fetus. Advise pregnant women of the potential risk to a fetus.

In the U.S. general population, the estimated background risk of major birth defects and miscarriage in clinically recognized pregnancies is 2-4% and 15-20%, respectively.

Data

Animal Data

Animal reproduction studies have not been conducted with KEYTRUDA to evaluate its effect on reproduction and fetal development. A literature-based assessment of the effects of the PD-1 pathway on reproduction demonstrated that a central function of the PD-1/PD-L1 pathway is to preserve pregnancy by maintaining maternal immune tolerance to the fetus. Blockade of PD-L1 signaling has been shown in murine models of pregnancy to disrupt tolerance to the fetus and to result in an increase in fetal loss; therefore, potential risks of administering KEYTRUDA during pregnancy include increased rates of abortion or stillbirth. As reported in the literature, there were no malformations related to the blockade of PD-1 signaling in the offspring of these animals; however, immune-mediated disorders occurred in PD-1 knockout mice. Based on its mechanism of action, fetal exposure to pembrolizumab may increase the risk of developing immune-mediated disorders or of altering the normal immune response.

8.2 Lactation

Risk Summary

There are no data on the presence of pembrolizumab in either animal or human milk or its effects on the breastfed child or on milk production. Maternal IgG is known to be present in human milk. The effects of local gastrointestinal exposure and limited systemic exposure in the breastfed child to KEYTRUDA are unknown. Because of the potential for serious adverse reactions in breastfed children, advise women not to breastfeed during treatment with KEYTRUDA and for 4 months after the last dose.

8.3 Females and Males of Reproductive Potential

Pregnancy Testing

Verify pregnancy status in females of reproductive potential prior to initiating KEYTRUDA [see Use in Specific Populations (8.1)].

Contraception

KEYTRUDA can cause fetal harm when administered to a pregnant woman [see Warnings and Precautions (5.5), Use in Specific Populations (8.1)]. Advise females of reproductive potential to use effective contraception during treatment with KEYTRUDA and for 4 months after the last dose.

8.4 Pediatric Use

The safety and effectiveness of KEYTRUDA as a single agent have been established in pediatric patients with melanoma, cHL, PMBCL, MCC, MSI-H or dMMR cancer, and TMB-H cancer. Use of KEYTRUDA in pediatric patients for these indications is supported by evidence from adequate and well-controlled studies in adults with additional pharmacokinetic and safety data in pediatric patients [see Adverse Reactions (6.1), Clinical Pharmacology (12.3), Clinical Studies (14.1, 14.5, 14.6, 14.8, 14.15, 14.18)].

In KEYNOTE-051, 173 pediatric patients (65 pediatric patients aged 6 months to younger than 12 years and 108 pediatric patients aged 12 to 17 years) with advanced melanoma, lymphoma, or PD-L1 positive or MSI-H solid tumors received KEYTRUDA 2 mg/kg every 3 weeks. The median duration of exposure was 2.1 months (range: 1 day to 25 months). Adverse reactions that occurred at a ≥10% higher rate in pediatric patients when compared to adults included pyrexia (33%), vomiting (29%), headache (25%), abdominal pain (23%), decreased lymphocyte count (13%), and decreased white blood cell count (11%). Laboratory abnormalities that occurred at a ≥10% higher rate in pediatric patients when compared to adults were leukopenia (30%), neutropenia (28%), thrombocytopenia (22%), and Grade 3 anemia (17%).

The safety and effectiveness of KEYTRUDA in pediatric patients have not been established in the other approved indications [see Indications and Usage (1)].

8.5 Geriatric Use

Of 3781 patients with melanoma, NSCLC, HNSCC, or urothelial carcinoma who were treated with KEYTRUDA in clinical studies, 48% were 65 years and over and 17% were 75 years and over. No overall differences in safety or effectiveness were observed between elderly patients and younger patients.

Of 389 adult patients with cHL who were treated with KEYTRUDA in clinical studies, 46 (12%) were 65 years and over. Patients aged 65 years and over had a higher incidence of serious adverse reactions (50%) than patients aged younger than 65 years (24%). Clinical studies of KEYTRUDA in cHL did not include sufficient numbers of patients aged 65 years and over to determine whether effectiveness differs from that in younger patients.

Of 506 adult patients with Stage IB (T2a ≥4 cm), II, or IIIA NSCLC following complete resection and platinum-based chemotherapy who were treated with KEYTRUDA in KEYNOTE-091, 242 (48%) were 65 years and over. No overall differences in safety or effectiveness were observed between elderly patients and younger patients.

Of 596 adult patients with TNBC who were treated with KEYTRUDA in combination with paclitaxel, paclitaxel protein-bound, or gemcitabine and carboplatin in KEYNOTE-355, 137 (23%) were 65 years and over. No overall differences in safety or effectiveness were observed between elderly patients and younger patients.

Of 406 adult patients with endometrial carcinoma who were treated with KEYTRUDA in combination with lenvatinib in KEYNOTE-775, 201 (50%) were 65 years and over. No overall differences in safety or effectiveness were observed between elderly patients and younger patients.

Of the 564 patients with locally advanced or metastatic urothelial cancer treated with KEYTRUDA in combination with enfortumab vedotin, 44% (n=247) were 65-74 years and 26% (n=144) were 75 years or older. No overall differences in effectiveness were observed between patients 65 years of age or older and younger patients. Patients 75 years of age or older treated with KEYTRUDA in combination with enfortumab vedotin experienced a higher incidence of fatal adverse reactions than younger patients. The incidence of fatal adverse reactions was 4% in patients younger than 75 and 7% in patients 75 years or older.

Of the 167 patients with MIBC treated with KEYTRUDA in combination with enfortumab vedotin, 37% (n=61) were 65-74 years and 46% (n=77) were 75 years or older. Patients 75 years of age or older treated with KEYTRUDA in combination with enfortumab vedotin experienced a higher incidence of fatal adverse reactions than younger patients. The incidence of fatal adverse reactions was 4% in patients younger than 75 and 12% in patients 75 years or older.

Of the 432 patients randomized to KEYTRUDA in combination with axitinib in the KEYNOTE-426 trial, 40% were 65 years or older. No overall difference in safety or efficacy was reported between patients who were ≥65 years of age and younger.

Of 294 adult patients with FIGO 2014 Stage III-IVA cervical cancer who were treated with KEYTRUDA in combination with CRT in KEYNOTE-A18, 42 (14%) were 65 years and over. No overall difference in safety was observed between patients ≥65 years of age and younger patients.

Of 643 adult patients with ovarian cancer who were treated with KEYTRUDA in combination with paclitaxel with or without bevacizumab in KEYNOTE-B96, 236 (37%) were 65 years and over and 58 (9%) were 75 years and over. No overall differences in safety or effectiveness were observed between patients ≥65 years of age and younger patients.

11 DESCRIPTION

Pembrolizumab is a programmed death receptor-1 (PD 1)-blocking antibody. Pembrolizumab is a humanized monoclonal IgG4 kappa antibody with an approximate molecular weight of 149 kDa. Pembrolizumab is produced in recombinant Chinese hamster ovary (CHO) cells.

KEYTRUDA (pembrolizumab) injection is a sterile, preservative-free, clear to slightly opalescent, colorless to slightly yellow solution for intravenous use. Each vial contains 100 mg of pembrolizumab in 4 mL of solution. Each 1 mL of solution contains 25 mg of pembrolizumab and is formulated in: L-histidine (1.55 mg), polysorbate 80 (0.2 mg), sucrose (70 mg), and Water for Injection, USP.

12 CLINICAL PHARMACOLOGY

12.1 Mechanism of Action

Binding of the PD-1 ligands, PD-L1 and PD-L2, to the PD-1 receptor found on T cells, inhibits T cell proliferation and cytokine production. Upregulation of PD-1 ligands occurs in some tumors and signaling through this pathway can contribute to inhibition of active T-cell immune surveillance of tumors. Pembrolizumab is a monoclonal antibody that binds to the PD-1 receptor and blocks its interaction with PD-L1 and PD-L2, releasing PD-1 pathway-mediated inhibition of the immune response, including the anti-tumor immune response. In syngeneic mouse tumor models, blocking PD-1 activity resulted in decreased tumor growth.

In syngeneic mouse tumor models, combination treatment of a PD-1 blocking antibody and kinase inhibitor lenvatinib decreased tumor-associated macrophages, increased activated cytotoxic T cells, and reduced tumor growth compared to either treatment alone.

12.2 Pharmacodynamics

There are no clinically significant exposure-response relationships for efficacy or safety at pembrolizumab dosages of 200 mg or 2 mg/kg every 3 weeks and 400 mg every 6 weeks regardless of cancer type based on observed data in adult patients with melanoma, cHL, and PMBCL.

12.3 Pharmacokinetics

The pharmacokinetics (PK) of pembrolizumab was characterized using a population PK analysis with concentration data collected from 2993 patients with various cancers who received pembrolizumab doses of 1 to 10 mg/kg every 2 weeks, 2 to 10 mg/kg every 3 weeks, or 200 mg every 3 weeks.

Steady-state concentrations of pembrolizumab were reached by 16 weeks of repeated dosing with an every 3-week regimen and the systemic accumulation was 2.1-fold. The peak concentration (Cmax), trough concentration (Cmin), and area under the plasma concentration versus time curve at steady state (AUCss) of pembrolizumab increased dose proportionally in the dose range of 2 to 10 mg/kg every 3 weeks.

Distribution

The geometric mean value (CV%) for volume of distribution at steady state is 6.0 L (20%).

Elimination

Pembrolizumab clearance (CV%) is approximately 23% lower [geometric mean, 195 mL/day (40%)] at steady state than that after the first dose [252 mL/day (37%)]; this decrease in clearance with time is not considered clinically important. The terminal half-life (t1/2) is 22 days (32%).

Specific Populations

The following factors had no clinically important effect on the CL of pembrolizumab: age (range: 15 to 94 years), sex, race (89% White), renal impairment (eGFR ≥15 mL/min/1.73 m^2), mild to moderate hepatic impairment (total bilirubin ≤3 times ULN and any AST), or tumor burden. The impact of severe hepatic impairment (total bilirubin >3 times ULN and any AST) on the pharmacokinetics of pembrolizumab is unknown.

Pediatric Patients: Pembrolizumab concentrations with weight-based dosing at 2 mg/kg every 3 weeks in pediatric patients (10 months to 17 years) are comparable to those of adults at the same dose.

12.6 Immunogenicity

The observed incidence of anti-drug antibodies (ADA) is highly dependent on the sensitivity and specificity of the assay. Differences in assay methods preclude meaningful comparisons of the incidence of ADA in the studies described in this section with the incidence of ADA in other studies, including those of KEYTRUDA or of other pembrolizumab products.

Trough levels of pembrolizumab interfere with the electrochemiluminescent (ECL) assay results; therefore, a subset analysis was performed in the KEYTRUDA-treated patients with a pembrolizumab concentration below the drug tolerance level of the ADA assay.

In clinical studies in patients treated with KEYTRUDA at a dosage of 2 mg/kg every 3 weeks, 200 mg every 3 weeks, or 10 mg/kg every 2 or 3 weeks, 27 (2.1%) of 1,289 evaluable patients tested positive for treatment-emergent anti-pembrolizumab antibodies of whom 6 (0.5%) patients had neutralizing antibodies against pembrolizumab. There were no identified clinically significant effects of ADA on pembrolizumab pharmacokinetics or on the risk of infusion reactions. Because of the low occurrence of ADA, the effect of these ADA on the effectiveness of KEYTRUDA is unknown.

13 NONCLINICAL TOXICOLOGY

13.1 Carcinogenesis, Mutagenesis, Impairment of Fertility

No studies have been performed to test the potential of pembrolizumab for carcinogenicity or genotoxicity.

Fertility studies have not been conducted with pembrolizumab. In 1-month and 6-month repeat-dose toxicology studies in monkeys, there were no notable effects in the male and female reproductive organs; however, most animals in these studies were not sexually mature.

13.2 Animal Toxicology and/or Pharmacology

In animal models, inhibition of PD-1/PD-L1 signaling increased the severity of some infections and enhanced inflammatory responses. Mycobacterium tuberculosis-infected PD-1 knockout mice exhibit markedly decreased survival compared with wild-type controls, which correlated with increased bacterial proliferation and inflammatory responses in these animals. PD-1 blockade using a primate anti-PD-1 antibody was also shown to exacerbate M. tuberculosis infection in rhesus macaques. PD-1 and PD-L1 knockout mice and mice receiving PD-L1-blocking antibody have also shown decreased survival following infection with lymphocytic choriomeningitis virus. Administration of pembrolizumab in chimpanzees with naturally occurring chronic hepatitis B infection resulted in two out of four animals with significantly increased levels of serum ALT, AST, and GGT, which persisted for at least 1 month after discontinuation of pembrolizumab.

14 CLINICAL STUDIES

14.1 Melanoma

Ipilimumab-Naive Melanoma

The efficacy of KEYTRUDA was investigated in KEYNOTE-006 (NCT01866319), a randomized (1:1:1), open-label, multicenter, active-controlled trial in 834 patients. Patients were randomized to receive KEYTRUDA at a dose of 10 mg/kg intravenously every 2 weeks or 10 mg/kg intravenously every 3 weeks until disease progression or unacceptable toxicity or to ipilimumab 3 mg/kg intravenously every 3 weeks for 4 doses unless discontinued earlier for disease progression or unacceptable toxicity. Patients with disease progression could receive additional doses of treatment unless disease progression was symptomatic, was rapidly progressive, required urgent intervention, occurred with a decline in performance status, or was confirmed at 4 to 6 weeks with repeat imaging. Randomization was stratified by line of therapy (0 vs. 1), ECOG PS (0 vs. 1), and PD-L1 expression (≥1% of tumor cells [positive] vs. <1% of tumor cells [negative]) according to an investigational use only (IUO) assay. Key eligibility criteria were unresectable or metastatic melanoma; no prior ipilimumab; and no more than one prior systemic treatment for metastatic melanoma. Patients with BRAF V600E mutation-positive melanoma were not required to have received prior BRAF inhibitor therapy. Patients with autoimmune disease; a medical condition that required immunosuppression; previous severe hypersensitivity to other monoclonal antibodies; and HIV, hepatitis B or hepatitis C infection, were ineligible. Assessment of tumor status was performed at 12 weeks, then every 6 weeks through Week 48, followed by every 12 weeks thereafter. The major efficacy outcome measures were overall survival (OS) and progression-free survival (PFS; as assessed by blinded independent central review [BICR] using Response Evaluation Criteria in Solid Tumors [RECIST v1.1, modified to follow a maximum of 10 target lesions and a maximum of 5 target lesions per organ]). Additional efficacy outcome measures were objective response rate (ORR) and duration of response (DoR).

The study population characteristics were: median age of 62 years (range: 18 to 89); 60% male; 98% White; 66% had no prior systemic therapy for metastatic disease; 69% ECOG PS of 0; 80% had PD-L1 positive melanoma, 18% had PD-L1 negative melanoma, and 2% had unknown PD-L1 status using the IUO assay; 65% had M1c stage disease; 68% with normal LDH; 36% with reported BRAF mutation-positive melanoma; and 9% with a history of brain metastases. Among patients with BRAF mutation-positive melanoma, 139 (46%) were previously treated with a BRAF inhibitor.

The study demonstrated statistically significant improvements in OS and PFS for patients randomized to KEYTRUDA as compared to ipilimumab. Among the 91 patients randomized to KEYTRUDA 10 mg/kg every 3 weeks with an objective response, response durations ranged from 1.4+ to 8.1+ months. Among the 94 patients randomized to KEYTRUDA 10 mg/kg every 2 weeks with an objective response, response durations ranged from 1.4+ to 8.2 months. Efficacy results are summarized in Table 61 and Figure 1.

Table 61: Efficacy Results in KEYNOTE-006
Endpoint | KEYTRUDA 10 mg/kg every 3 weeks n=277 | KEYTRUDA 10 mg/kg every 2 weeks n=279 | Ipilimumab 3 mg/kg every 3 weeks n=278
OS
Deaths (%) | 92 (33%) | 85 (30%) | 112 (40%)
Hazard ratio [Hazard ratio (KEYTRUDA compared to ipilimumab) based on the stratified Cox proportional hazard model] (95% CI) | 0.69 (0.52, 0.90) | 0.63 (0.47, 0.83) | ---
p-Value (stratified log-rank) | 0.004 | <0.001 | ---
PFS by BICR
Events (%) | 157 (57%) | 157 (56%) | 188 (68%)
Median in months (95% CI) | 4.1 (2.9, 6.9) | 5.5 (3.4, 6.9) | 2.8 (2.8, 2.9)
Hazard ratio (95% CI) | 0.58 (0.47, 0.72) | 0.58 (0.46, 0.72) | ---
p-Value (stratified log-rank) | <0.001 | <0.001 | ---
Best objective response by BICR
ORR (95% CI) | 33% (27, 39) | 34% (28, 40) | 12% (8, 16)
Complete response rate | 6% | 5% | 1%
Partial response rate | 27% | 29% | 10%

Figure 1: Kaplan-Meier Curve for Overall Survival in KEYNOTE-006 [Based on the final analysis with an additional follow-up of 9 months (total of 383 deaths as pre-specified in the protocol)]

Ipilimumab-Refractory Melanoma

The efficacy of KEYTRUDA was investigated in KEYNOTE-002 (NCT01704287), a multicenter, randomized (1:1:1), active-controlled trial in 540 patients randomized to receive one of two doses of KEYTRUDA in a blinded fashion or investigator's choice chemotherapy. The treatment arms consisted of KEYTRUDA 2 mg/kg or 10 mg/kg intravenously every 3 weeks or investigator's choice of any of the following chemotherapy regimens: dacarbazine 1000 mg/m^2 intravenously every 3 weeks (26%), temozolomide 200 mg/m^2 orally once daily for 5 days every 28 days (25%), carboplatin AUC 6 mg/mL/min intravenously plus paclitaxel 225 mg/m^2 intravenously every 3 weeks for four cycles then carboplatin AUC of 5 mg/mL/min plus paclitaxel 175 mg/m^2 every 3 weeks (25%), paclitaxel 175 mg/m^2 intravenously every 3 weeks (16%), or carboplatin AUC 5 or 6 mg/mL/min intravenously every 3 weeks (8%). Randomization was stratified by ECOG PS (0 vs. 1), LDH levels (normal vs. elevated [≥110% ULN]) and BRAF V600 mutation status (wild-type [WT] or V600E). The trial included patients with unresectable or metastatic melanoma with progression of disease; refractory to two or more doses of ipilimumab (3 mg/kg or higher) and, if BRAF V600 mutation-positive, a BRAF or MEK inhibitor; and disease progression within 24 weeks following the last dose of ipilimumab. The trial excluded patients with uveal melanoma and active brain metastasis. Patients received KEYTRUDA until unacceptable toxicity; disease progression that was symptomatic, was rapidly progressive, required urgent intervention, occurred with a decline in performance status, or was confirmed at 4 to 6 weeks with repeat imaging; withdrawal of consent; or physician's decision to stop therapy for the patient. Assessment of tumor status was performed at 12 weeks after randomization, then every 6 weeks through week 48, followed by every 12 weeks thereafter. Patients on chemotherapy who experienced progression of disease were offered KEYTRUDA. The major efficacy outcomes were PFS as assessed by BICR per RECIST v1.1, modified to follow a maximum of 10 target lesions and a maximum of 5 target lesions per organ, and OS. Additional efficacy outcome measures were confirmed ORR as assessed by BICR per RECIST v1.1, modified to follow a maximum of 10 target lesions and a maximum of 5 target lesions per organ, and DoR.

The study population characteristics were: median age of 62 years (range: 15 to 89), 43% age 65 or older; 61% male; 98% White; and 55% ECOG PS of 0 and 45% ECOG PS of 1. Twenty-three percent of patients were BRAF V600 mutation positive, 40% had elevated LDH at baseline, 82% had M1c disease, and 73% had two or more prior therapies for advanced or metastatic disease.

The study demonstrated a statistically significant improvement in PFS for patients randomized to KEYTRUDA as compared to control arm. There was no statistically significant difference between KEYTRUDA 2 mg/kg and chemotherapy or between KEYTRUDA 10 mg/kg and chemotherapy in the OS analysis in which 55% of the patients who had been randomized to receive chemotherapy had crossed over to receive KEYTRUDA. Among the 38 patients randomized to KEYTRUDA 2 mg/kg with an objective response, response durations ranged from 1.3+ to 11.5+ months. Among the 46 patients randomized to KEYTRUDA 10 mg/kg with an objective response, response durations ranged from 1.1+ to 11.1+ months. Efficacy results are summarized in Table 62 and Figure 2.

Table 62: Efficacy Results in KEYNOTE-002
Endpoint | KEYTRUDA 2 mg/kg every 3 weeks | KEYTRUDA 10 mg/kg every 3 weeks | Chemotherapy
 | n=180 | n=181 | n=179
PFS
Number of Events, n (%) | 129 (72%) | 126 (70%) | 155 (87%)
Progression, n (%) | 105 (58%) | 107 (59%) | 134 (75%)
Death, n (%) | 24 (13%) | 19 (10%) | 21 (12%)
Median in months (95% CI) | 2.9 (2.8, 3.8) | 2.9 (2.8, 4.7) | 2.7 (2.5, 2.8)
p-Value (stratified log-rank) | <0.001 | <0.001 | ---
Hazard ratio [Hazard ratio (KEYTRUDA compared to chemotherapy) based on the stratified Cox proportional hazard model] (95% CI) | 0.57 (0.45, 0.73) | 0.50 (0.39, 0.64) | ---
OS [With additional follow-up of 18 months after the PFS analysis]
Deaths (%) | 123 (68%) | 117 (65%) | 128 (72%)
Hazard ratio (95% CI) | 0.86 (0.67, 1.10) | 0.74 (0.57, 0.96) | ---
p-Value (stratified log-rank) | 0.117 | 0.011 [Not statistically significant compared to multiplicity adjusted significance level of 0.01] | ---
Median in months (95% CI) | 13.4 (11.0, 16.4) | 14.7 (11.3, 19.5) | 11.0 (8.9, 13.8)
Objective Response Rate
ORR (95% CI) | 21% (15, 28) | 25% (19, 32) | 4% (2, 9)
Complete response rate | 2% | 3% | 0%
Partial response rate | 19% | 23% | 4%

Figure 2: Kaplan-Meier Curve for Progression-Free Survival in KEYNOTE-002

Adjuvant Treatment of Resected Stage IIB or IIC Melanoma

The efficacy of KEYTRUDA was investigated in KEYNOTE-716 (NCT03553836), a multicenter, randomized (1:1), double-blind, placebo-controlled trial in patients with completely resected Stage IIB or IIC melanoma. Patients were randomized to KEYTRUDA 200 mg or the pediatric (≥12 years old) dose of KEYTRUDA 2 mg/kg intravenously (up to a maximum of 200 mg) every three weeks or placebo for up to one year until disease recurrence or unacceptable toxicity. Randomization was stratified by AJCC 8th edition T Stage (>2.0-4.0 mm with ulceration vs. >4.0 mm without ulceration vs. >4.0 mm with ulceration). Patients must not have been previously treated for melanoma beyond complete surgical resection for their melanoma prior to study entry. The major efficacy outcome measure was investigator-assessed recurrence-free survival (RFS) (defined as the time between the date of randomization and the date of first recurrence [local, in-transit or regional lymph nodes or distant recurrence] or death, whichever occurred first). New primary melanomas were excluded from the definition of RFS. Distant metastasis-free survival (DMFS), defined as a spread of tumor to distant organs or distant lymph nodes, was an additional efficacy outcome measure. Patients underwent imaging every six months for one year from randomization, every 6 months from years 2 to 4, and then once in year 5 from randomization or until recurrence, whichever came first.

The study population characteristics were: median age of 61 years (range: 16 to 87), 39% age 65 or older; 60% male; 98% White; and 93% ECOG PS of 0 and 7% ECOG PS of 1. Sixty-four percent had Stage IIB and 35% had Stage IIC.

The trial demonstrated a statistically significant improvement in RFS and DMFS for patients randomized to the KEYTRUDA arm compared with placebo. Efficacy results are summarized in Table 63 and Figure 3.

Table 63: Efficacy Results in KEYNOTE-716
Endpoint | KEYTRUDA 200 mg every 3 weeks n=487 | Placebo n=489
RFS
Number (%) of patients with event | 54 (11%) | 82 (17%)
Median in months (95% CI) | NR (22.6, NR) | NR (NR, NR)
Hazard ratio [Based on the stratified Cox proportional hazard model] , [Based on a log-rank test stratified by American Joint Committee on Cancer 8th edition (AJCC) stage] (95% CI) | 0.65 (0.46, 0.92)
p-Value | 0.0132 [p-Value is compared with 0.0202 of the allocated alpha for this interim analysis.]
DMFS
Number (%) of patients with event | 63 (13%) | 95 (19%)
Median in months (95% CI) | NR (NR, NR) | NR (NR, NR)
Hazard ratio, (95% CI) | 0.64 (0.47, 0.88)
p-Value | 0.0058 [p-Value is compared with 0.0256 of the allocated alpha for this interim analysis.]
NR = not reached

Figure 3: Kaplan-Meier Curve for Recurrence-Free Survival in KEYNOTE-716

Adjuvant Treatment of Stage III Resected Melanoma

The efficacy of KEYTRUDA was investigated in KEYNOTE-054 (NCT02362594), a multicenter, randomized (1:1), double-blind, placebo-controlled trial in patients with completely resected Stage IIIA (>1 mm lymph node metastasis), IIIB, or IIIC melanoma. Patients were randomized to KEYTRUDA 200 mg intravenously every three weeks or placebo for up to one year until disease recurrence or unacceptable toxicity. Randomization was stratified by American Joint Committee on Cancer 7th edition (AJCC) stage (IIIA vs. IIIB vs. IIIC 1-3 positive lymph nodes vs. IIIC ≥4 positive lymph nodes) and geographic region (North America, European countries, Australia, and other countries as designated). Patients must have undergone lymph node dissection and, if indicated, radiotherapy within 13 weeks prior to starting treatment. The major efficacy outcome measure was investigator-assessed recurrence-free survival (RFS) in the whole population and in the population with PD-L1 positive tumors where RFS was defined as the time between the date of randomization and the date of first recurrence (local, regional, or distant metastasis) or death, whichever occurs first. New primary melanomas were excluded from the definition of RFS. DMFS in the whole population and in the population with PD-L1 positive tumors were additional efficacy outcome measures. DMFS was defined as a spread of tumor to distant organs or distant lymph nodes. Patients underwent imaging every 12 weeks after the first dose of KEYTRUDA for the first two years, then every 6 months from year 3 to 5, and then annually.

The study population characteristics were: median age of 54 years (range: 19 to 88), 25% age 65 or older; 62% male; and 94% ECOG PS of 0 and 6% ECOG PS of 1. Sixteen percent had Stage IIIA, 46% had Stage IIIB, 18% had Stage IIIC (1-3 positive lymph nodes), and 20% had Stage IIIC (≥4 positive lymph nodes); 50% were BRAF V600 mutation positive and 44% were BRAF wild-type; and 84% had PD-L1 positive melanoma with TPS ≥1% according to an IUO assay.

The trial demonstrated a statistically significant improvement in RFS and DMFS for patients randomized to the KEYTRUDA arm compared with placebo. Efficacy results are summarized in Table 64 and Figure 4.

Table 64: Efficacy Results in KEYNOTE-054
Endpoint | KEYTRUDA 200 mg every 3 weeks n=514 | Placebo n=505
RFS
Number (%) of patients with event | 135 (26%) | 216 (43%)
Median in months (95% CI) | NR | 20.4 (16.2, NR)
Hazard ratio [Based on the stratified Cox proportional hazard model] , [Stratified by American Joint Committee on Cancer 7th edition (AJCC) stage] (95% CI) | 0.57 (0.46, 0.70)
p-Value (log-rank) | <0.001 [p-Value is compared with 0.016 of the allocated alpha for this interim analysis.]
DMFS
Number (%) of patients with event | 173 (34%) | 245 (49%)
Median in months (95% CI) | NR (49.6, NR) | 40.0 (27.7, NR)
Hazard ratio, (95% CI) | 0.60 (0.49, 0.73)
p-Value (log-rank) | <0.0001 [p-Value is compared with 0.028 of the allocated alpha for this analysis.]
NR = not reached

For patients with PD-L1 positive tumors, the RFS HR was 0.54 (95% CI: 0.42, 0.69); p<0.0001. For patients with PD-L1 positive tumors, the DMFS HR was 0.61 (95% CI: 0.49, 0.76); p<0.0001. The RFS and DMFS benefit for KEYTRUDA compared to placebo was observed regardless of tumor PD-L1 expression.

Figure 4: Kaplan-Meier Curve for Recurrence-Free Survival in KEYNOTE-054

14.2 Non-Small Cell Lung Cancer

First-line treatment of metastatic nonsquamous NSCLC with pemetrexed and platinum chemotherapy

The efficacy of KEYTRUDA in combination with pemetrexed and platinum chemotherapy was investigated in KEYNOTE-189 (NCT02578680), a randomized, multicenter, double-blind, active-controlled trial conducted in 616 patients with metastatic nonsquamous NSCLC, regardless of PD-L1 tumor expression status, who had not previously received systemic therapy for metastatic disease and in whom there were no EGFR or ALK genomic tumor aberrations. Patients with autoimmune disease that required systemic therapy within 2 years of treatment; a medical condition that required immunosuppression; or who had received more than 30 Gy of thoracic radiation within the prior 26 weeks were ineligible. Randomization was stratified by smoking status (never vs. former/current), choice of platinum (cisplatin vs. carboplatin), and tumor PD-L1 status (TPS <1% [negative] vs. TPS ≥1%). Patients were randomized (2:1) to one of the following treatment arms:

- KEYTRUDA 200 mg, pemetrexed 500 mg/m^2, and investigator's choice of cisplatin 75 mg/m^2 or carboplatin AUC 5 mg/mL/min intravenously on Day 1 of each 21-day cycle for 4 cycles followed by KEYTRUDA 200 mg and pemetrexed 500 mg/m^2 intravenously every 3 weeks. KEYTRUDA was administered prior to chemotherapy on Day 1.
- Placebo, pemetrexed 500 mg/m^2, and investigator's choice of cisplatin 75 mg/m^2 or carboplatin AUC 5 mg/mL/min intravenously on Day 1 of each 21-day cycle for 4 cycles followed by placebo and pemetrexed 500 mg/m^2 intravenously every 3 weeks.

Treatment with KEYTRUDA continued until RECIST v1.1 (modified to follow a maximum of 10 target lesions and a maximum of 5 target lesions per organ)-defined progression of disease as determined by the investigator, unacceptable toxicity, or a maximum of 24 months. Administration of KEYTRUDA was permitted beyond RECIST-defined disease progression if the patient was clinically stable and considered to be deriving clinical benefit by the investigator. Patients randomized to placebo and chemotherapy were offered KEYTRUDA as a single agent at the time of disease progression. Assessment of tumor status was performed at Week 6, Week 12, and then every 9 weeks thereafter. The main efficacy outcome measures were OS and PFS as assessed by BICR according to RECIST v1.1, modified to follow a maximum of 10 target lesions and a maximum of 5 target lesions per organ. Additional efficacy outcome measures were ORR and DoR, as assessed by BICR according to RECIST v1.1, modified to follow a maximum of 10 target lesions and a maximum of 5 target lesions per organ.

The study population characteristics were: median age of 64 years (range: 34 to 84), 49% age 65 or older; 59% male; 94% White and 3% Asian; 56% ECOG PS of 1; and 18% with history of brain metastases. Thirty-one percent had tumor PD-L1 expression TPS <1% [negative]. Seventy-two percent received carboplatin and 12% were never smokers. A total of 85 patients in the placebo and chemotherapy arm received an anti-PD-1/PD-L1 monoclonal antibody at the time of disease progression.

The trial demonstrated a statistically significant improvement in OS and PFS for patients randomized to KEYTRUDA in combination with pemetrexed and platinum chemotherapy compared with placebo, pemetrexed, and platinum chemotherapy. Table 65 and Figure 5 summarize the efficacy results for KEYNOTE-189.

Table 65: Efficacy Results in KEYNOTE-189
Endpoint | KEYTRUDA 200 mg every 3 weeks Pemetrexed Platinum Chemotherapy n=410 | Placebo Pemetrexed Platinum Chemotherapy n=206
OS
Number (%) of patients with event | 127 (31%) | 108 (52%)
Median in months (95% CI) | NR (NR, NR) | 11.3 (8.7, 15.1)
Hazard ratio [Based on the stratified Cox proportional hazard model] (95% CI) | 0.49 (0.38, 0.64)
p-Value [Based on a stratified log-rank test] | <0.0001
PFS
Number of patients with event (%) | 245 (60%) | 166 (81%)
Median in months (95% CI) | 8.8 (7.6, 9.2) | 4.9 (4.7, 5.5)
Hazard ratio (95% CI) | 0.52 (0.43, 0.64)
p-Value | <0.0001
Objective Response Rate
ORR [Response: Best objective response as confirmed complete response or partial response] (95% CI) | 48% (43, 53) | 19% (14, 25)
Complete response | 0.5% | 0.5%
Partial response | 47% | 18%
p-Value [Based on Miettinen and Nurminen method stratified by PD-L1 status, platinum chemotherapy, and smoking status] | <0.0001
Duration of Response
Median in months (range) | 11.2 (1.1+, 18.0+) | 7.8 (2.1+, 16.4+)
NR = not reached

At the protocol-specified final OS analysis, the median in the KEYTRUDA in combination with pemetrexed and platinum chemotherapy arm was 22.0 months (95% CI: 19.5, 24.5) compared to 10.6 months (95% CI: 8.7, 13.6) in the placebo with pemetrexed and platinum chemotherapy arm, with an HR of 0.56 (95% CI: 0.46, 0.69).

Figure 5: Kaplan-Meier Curve for Overall Survival in KEYNOTE-189 [Based on the protocol-specified final OS analysis]

First-line treatment of metastatic squamous NSCLC with carboplatin and either paclitaxel or paclitaxel protein-bound chemotherapy

The efficacy of KEYTRUDA in combination with carboplatin and investigator's choice of either paclitaxel or paclitaxel protein-bound was investigated in KEYNOTE-407 (NCT02775435), a randomized, multi-center, double-blind, placebo-controlled trial conducted in 559 patients with metastatic squamous NSCLC, regardless of PD-L1 tumor expression status, who had not previously received systemic therapy for metastatic disease. Patients with autoimmune disease that required systemic therapy within 2 years of treatment; a medical condition that required immunosuppression; or who had received more than 30 Gy of thoracic radiation within the prior 26 weeks were ineligible. Randomization was stratified by tumor PD-L1 status (TPS <1% [negative] vs. TPS ≥1%), choice of paclitaxel or paclitaxel protein-bound, and geographic region (East Asia vs. non-East Asia). Patients were randomized (1:1) to one of the following treatment arms; all study medications were administered via intravenous infusion:

- KEYTRUDA 200 mg and carboplatin AUC 6 mg/mL/min on Day 1 of each 21-day cycle for 4 cycles, and paclitaxel 200 mg/m^2 on Day 1 of each 21-day cycle for 4 cycles or paclitaxel protein-bound 100 mg/m^2 on Days 1, 8 and 15 of each 21-day cycle for 4 cycles, followed by KEYTRUDA 200 mg every 3 weeks. KEYTRUDA was administered prior to chemotherapy on Day 1.
- Placebo and carboplatin AUC 6 mg/mL/min on Day 1 of each 21-day cycle for 4 cycles and paclitaxel 200 mg/m^2 on Day 1 of each 21-day cycle for 4 cycles or paclitaxel protein-bound 100 mg/m^2 on Days 1, 8 and 15 of each 21-day cycle for 4 cycles, followed by placebo every 3 weeks.

Treatment with KEYTRUDA and chemotherapy or placebo and chemotherapy continued until RECIST v1.1 (modified to follow a maximum of 10 target lesions and a maximum of 5 target lesions per organ)-defined progression of disease as determined by BICR, unacceptable toxicity, or a maximum of 24 months. Administration of KEYTRUDA was permitted beyond RECIST-defined disease progression if the patient was clinically stable and deriving clinical benefit as determined by the investigator. Patients randomized to the placebo and chemotherapy arm were offered KEYTRUDA as a single agent at the time of disease progression. Assessment of tumor status was performed every 6 weeks through Week 18, every 9 weeks through Week 45 and every 12 weeks thereafter. The main efficacy outcome measures were PFS and ORR as assessed by BICR using RECIST v1.1, modified to follow a maximum of 10 target lesions and a maximum of 5 target lesions per organ, and OS. An additional efficacy outcome measure was DoR as assessed by BICR according to RECIST v1.1, modified to follow a maximum of 10 target lesions and a maximum of 5 target lesions per organ.

The study population characteristics were: median age of 65 years (range: 29 to 88), 55% age 65 or older; 81% male; 77% White; 71% ECOG PS of 1; and 8% with a history of brain metastases. Thirty-five percent had tumor PD-L1 expression TPS <1%; 19% were from the East Asian region; and 60% received paclitaxel.

The trial demonstrated a statistically significant improvement in OS, PFS and ORR in patients randomized to KEYTRUDA in combination with carboplatin and either paclitaxel or paclitaxel protein-bound chemotherapy compared with patients randomized to placebo with carboplatin and either paclitaxel or paclitaxel protein-bound chemotherapy. Table 66 and Figure 6 summarize the efficacy results for KEYNOTE-407.

Table 66: Efficacy Results in KEYNOTE-407
Endpoint | KEYTRUDA 200 mg every 3 weeks Carboplatin Paclitaxel/Paclitaxel protein-bound n=278 | Placebo Carboplatin Paclitaxel/Paclitaxel protein-bound n=281
OS
Number of events (%) | 85 (31%) | 120 (43%)
Median in months (95% CI) | 15.9 (13.2, NE) | 11.3 (9.5, 14.8)
Hazard ratio [Based on the stratified Cox proportional hazard model] (95% CI) | 0.64 (0.49, 0.85)
p-Value [Based on a stratified log-rank test] | 0.0017
PFS
Number of events (%) | 152 (55%) | 197 (70%)
Median in months (95% CI) | 6.4 (6.2, 8.3) | 4.8 (4.2, 5.7)
Hazard ratio (95% CI) | 0.56 (0.45, 0.70)
p-Value | <0.0001
 | n=101 | n=103
Objective Response Rate [ORR primary analysis and DoR analysis were conducted with the first 204 patients enrolled.]
ORR (95% CI) | 58% (48, 68) | 35% (26, 45)
Difference (95% CI) | 23.6% (9.9, 36.4)
p-Value [Based on a stratified Miettinen-Nurminen test] | 0.0008
Duration of Response
Median duration of response in months (range) | 7.2 (2.4, 12.4+) | 4.9 (2.0, 12.4+)
NE = not estimable

At the protocol-specified final OS analysis, the median in the KEYTRUDA in combination with carboplatin and either paclitaxel or paclitaxel protein-bound chemotherapy arm was 17.1 months (95% CI: 14.4, 19.9) compared to 11.6 months (95% CI: 10.1, 13.7) in the placebo with carboplatin and either paclitaxel or paclitaxel protein-bound chemotherapy arm, with an HR of 0.71 (95% CI: 0.58, 0.88).

Figure 6: Kaplan-Meier Curve for Overall Survival in KEYNOTE-407 [Based on the protocol-specified final OS analysis]

First-line treatment of metastatic NSCLC with PD-L1 expression (TPS≥ 1%) as a single agent

KEYNOTE-042

The efficacy of KEYTRUDA was investigated in KEYNOTE-042 (NCT02220894), a randomized, multicenter, open-label, active-controlled trial conducted in 1274 patients with Stage III NSCLC who were not candidates for surgical resection or definitive chemoradiation, or patients with metastatic NSCLC. Only patients whose tumors expressed PD-L1 (TPS ≥1%) by an immunohistochemistry assay using the PD-L1 IHC 22C3 pharmDx assay and who had not received prior systemic treatment for metastatic NSCLC were eligible. Patients with EGFR or ALK genomic tumor aberrations; autoimmune disease that required systemic therapy within 2 years of treatment; a medical condition that required immunosuppression; or who had received more than 30 Gy of radiation in the thoracic region within the prior 26 weeks of initiation of study were ineligible. Randomization was stratified by ECOG PS (0 vs. 1), histology (squamous vs. nonsquamous), geographic region (East Asia vs. non-East Asia), and PD-L1 expression (TPS ≥50% vs. TPS 1 to 49%). Patients were randomized (1:1) to receive KEYTRUDA 200 mg intravenously every 3 weeks or investigator's choice of either of the following platinum-containing chemotherapy regimens:

- Pemetrexed 500 mg/m^2 every 3 weeks and carboplatin AUC 5 to 6 mg/mL/min every 3 weeks on Day 1 for a maximum of 6 cycles followed by optional pemetrexed 500 mg/m^2 every 3 weeks for patients with nonsquamous histologies;
- Paclitaxel 200 mg/m^2 every 3 weeks and carboplatin AUC 5 to 6 mg/mL/min every 3 weeks on Day 1 for a maximum of 6 cycles followed by optional pemetrexed 500 mg/m^2 every 3 weeks for patients with nonsquamous histologies.

Treatment with KEYTRUDA continued until RECIST v1.1 (modified to follow a maximum of 10 target lesions and a maximum of 5 target lesions per organ)-defined progression of disease, unacceptable toxicity, or a maximum of 24 months. Administration of KEYTRUDA was permitted beyond RECIST-defined disease progression if the patient was clinically stable and deriving clinical benefit as determined by the investigator. Treatment with KEYTRUDA could be reinitiated at the time of subsequent disease progression and administered for up to 12 months. Assessment of tumor status was performed every 9 weeks. The main efficacy outcome measure was OS in the subgroup of patients with TPS ≥50% NSCLC, the subgroup of patients with TPS ≥20% NSCLC, and the overall population with TPS ≥1% NSCLC. Additional efficacy outcome measures were PFS and ORR in the subgroup of patients with TPS ≥50% NSCLC, the subgroup of patients with TPS ≥20% NSCLC, and the overall population with TPS ≥1% NSCLC as assessed by BICR according to RECIST v1.1, modified to follow a maximum of 10 target lesions and a maximum of 5 target lesions per organ.

The study population characteristics were: median age of 63 years (range: 25 to 90), 45% age 65 or older; 71% male; and 64% White, 30% Asian, and 2% Black. Nineteen percent were Hispanic or Latino. Sixty-nine percent had ECOG PS of 1; 39% with squamous and 61% with nonsquamous histology; 87% had M1 disease and 13% had Stage IIIA (2%) or Stage IIIB (11%) and who were not candidates for surgical resection or definitive chemoradiation per investigator assessment; and 5% with treated brain metastases at baseline. Forty-seven percent of patients had TPS ≥50% NSCLC and 53% had TPS 1 to 49% NSCLC.

The trial demonstrated a statistically significant improvement in OS for patients (PD-L1 TPS ≥50%, TPS ≥20%, TPS ≥1%) randomized to KEYTRUDA as compared with chemotherapy. Table 67 and Figure 7 summarize the efficacy results in the subgroup of patients with TPS ≥50% and in all randomized patients with TPS ≥1%.

Table 67: Efficacy Results of All Randomized Patients (TPS ≥1% and TPS ≥50%) in KEYNOTE-042
 | TPS ≥1% |  | TPS ≥50%
Endpoint | KEYTRUDA 200 mg every 3 weeks | Chemotherapy | KEYTRUDA 200 mg every 3 weeks | Chemotherapy
Endpoint | n=637 | n=637 | n=299 | n=300
OS
Number of events (%) | 371 (58%) | 438 (69%) | 157 (53%) | 199 (66%)
Median in months (95% CI) | 16.7 (13.9, 19.7) | 12.1 (11.3, 13.3) | 20.0 (15.4, 24.9) | 12.2 (10.4, 14.2)
Hazard ratio [Based on the stratified Cox proportional hazard model] (95% CI) | 0.81 (0.71, 0.93) |  | 0.69 (0.56, 0.85)
p-Value [Based on a stratified log-rank test; compared to a p-Value boundary of 0.0291] | 0.0036 |  | 0.0006
PFS
Number of events (%) | 507 (80%) | 506 (79%) | 221 (74%) | 233 (78%)
Median in months (95% CI) | 5.4 (4.3, 6.2) | 6.5 (6.3, 7.0) | 6.9 (5.9, 9.0) | 6.4 (6.1, 6.9)
Hazard ratio, [Not evaluated for statistical significance as a result of the sequential testing procedure for the secondary endpoints] (95% CI) | 1.07 (0.94, 1.21) |  | 0.82 (0.68, 0.99)
p-Value | - |  | NS [Not significant compared to a p-Value boundary of 0.0291]
Objective Response Rate
ORR (95% CI) | 27% (24, 31) | 27% (23, 30) | 39% (33.9, 45.3) | 32% (26.8, 37.6)
Complete response rate | 0.5% | 0.5% | 0.7% | 0.3%
Partial response rate | 27% | 26% | 39% | 32%
Duration of Response
% with duration ≥12 months [Based on observed duration of response] | 47% | 16% | 42% | 17%
% with duration ≥18 months | 26% | 6% | 25% | 5%

The results of all efficacy outcome measures in the subgroup of patients with PD-L1 TPS ≥20% NSCLC were intermediate between the results of those with PD-L1 TPS ≥1% and those with PD-L1 TPS ≥50%. In a pre-specified exploratory subgroup analysis for patients with TPS 1-49% NSCLC, the median OS was 13.4 months (95% CI: 10.7, 18.2) for the pembrolizumab group and 12.1 months (95% CI: 11.0, 14.0) in the chemotherapy group, with an HR of 0.92 (95% CI: 0.77, 1.11).

Figure 7: Kaplan-Meier Curve for Overall Survival in all Randomized Patients in KEYNOTE-042 (TPS ≥1%)

KEYNOTE-024

The efficacy of KEYTRUDA was also investigated in KEYNOTE-024 (NCT02142738), a randomized, multicenter, open-label, active-controlled trial in 305 previously untreated patients with metastatic NSCLC. The study design was similar to that of KEYNOTE-042, except that only patients whose tumors had high PD-L1 expression (TPS of 50% or greater) by an immunohistochemistry assay using the PD-L1 IHC 22C3 pharmDx assay were eligible. Patients were randomized (1:1) to receive KEYTRUDA 200 mg intravenously every 3 weeks or investigator's choice of any of the following platinum-containing chemotherapy regimens:

- Pemetrexed 500 mg/m^2 every 3 weeks and carboplatin AUC 5 to 6 mg/mL/min every 3 weeks on Day 1 for 4 to 6 cycles followed by optional pemetrexed 500 mg/m^2 every 3 weeks for patients with nonsquamous histologies;
- Pemetrexed 500 mg/m^2 every 3 weeks and cisplatin 75 mg/m^2 every 3 weeks on Day 1 for 4 to 6 cycles followed by optional pemetrexed 500 mg/m^2 every 3 weeks for patients with nonsquamous histologies;
- Gemcitabine 1250 mg/m^2 on days 1 and 8 and cisplatin 75 mg/m^2 every 3 weeks on Day 1 for 4 to 6 cycles;
- Gemcitabine 1250 mg/m^2 on Days 1 and 8 and carboplatin AUC 5 to 6 mg/mL/min every 3 weeks on Day 1 for 4 to 6 cycles;
- Paclitaxel 200 mg/m^2 every 3 weeks and carboplatin AUC 5 to 6 mg/mL/min every 3 weeks on Day 1 for 4 to 6 cycles followed by optional pemetrexed maintenance (for nonsquamous histologies).

Patients randomized to chemotherapy were offered KEYTRUDA at the time of disease progression.

The main efficacy outcome measure was PFS as assessed by BICR according to RECIST v1.1, modified to follow a maximum of 10 target lesions and a maximum of 5 target lesions per organ. Additional efficacy outcome measures were OS and ORR as assessed by BICR according to RECIST v1.1, modified to follow a maximum of 10 target lesions and a maximum of 5 target lesions per organ.

The study population characteristics were: median age of 65 years (range: 33 to 90), 54% age 65 or older; 61% male; 82% White and 15% Asian; 65% with ECOG PS of 1; 18% with squamous and 82% with nonsquamous histology and 9% with history of brain metastases. A total of 66 patients in the chemotherapy arm received KEYTRUDA at the time of disease progression.

The trial demonstrated a statistically significant improvement in both PFS and OS for patients randomized to KEYTRUDA as compared with chemotherapy. Table 68 and Figure 8 summarize the efficacy results for KEYNOTE-024.

Table 68: Efficacy Results in KEYNOTE-024
Endpoint | KEYTRUDA 200 mg every 3 weeks | Chemotherapy
 | n=154 | n=151
PFS
Number (%) of patients with event | 73 (47%) | 116 (77%)
Median in months (95% CI) | 10.3 (6.7, NR) | 6.0 (4.2, 6.2)
Hazard ratio [Based on the stratified Cox proportional hazard model for the interim analysis] (95% CI) | 0.50 (0.37, 0.68)
p-Value (stratified log-rank) | <0.001
OS
Number (%) of patients with event | 44 (29%) | 64 (42%)
Median in months (95% CI) [Based on the protocol-specified final OS analysis conducted at 169 events, which occurred 14 months after the interim analysis.] | 30.0 (18.3, NR) | 14.2 (9.8, 19.0)
Hazard ratio (95% CI) | 0.60 (0.41, 0.89)
p-Value (stratified log-rank) | 0.005 [p-Value is compared with 0.0118 of the allocated alpha for the interim analysis]
Objective Response Rate
ORR (95% CI) | 45% (37, 53) | 28% (21, 36)
Complete response rate | 4% | 1%
Partial response rate | 41% | 27%
p-Value (Miettinen-Nurminen) | 0.001
Median duration of response in months (range) | NR (1.9+, 14.5+) | 6.3 (2.1+, 12.6+)
NR = not reached

Figure 8: Kaplan-Meier Curve for Overall Survival in KEYNOTE-024 [Based on the protocol-specified final OS analysis conducted at 169 events, which occurred 14 months after the interim analysis.]

Previously treated NSCLC with PD-L1 expression (TPS≥ 1%)

The efficacy of KEYTRUDA was investigated in KEYNOTE-010 (NCT01905657), a randomized, multicenter, open-label, active-controlled trial conducted in 1033 patients with metastatic NSCLC that had progressed following platinum-containing chemotherapy, and if appropriate, targeted therapy for EGFR or ALK genomic tumor aberrations. Eligible patients had PD-L1 expression TPS of 1% or greater by an immunohistochemistry assay using the PD-L1 IHC 22C3 pharmDx assay. Patients with autoimmune disease; a medical condition that required immunosuppression; or who had received more than 30 Gy of thoracic radiation within the prior 26 weeks were ineligible. Randomization was stratified by tumor PD-L1 expression (PD-L1 expression TPS ≥50% vs. PD-L1 expression TPS=1-49%), ECOG PS (0 vs. 1), and geographic region (East Asia vs. non-East Asia). Patients were randomized (1:1:1) to receive KEYTRUDA 2 mg/kg intravenously every 3 weeks, KEYTRUDA 10 mg/kg intravenously every 3 weeks or docetaxel intravenously 75 mg/m^2 every 3 weeks until unacceptable toxicity or disease progression. Patients randomized to KEYTRUDA were permitted to continue until disease progression that was symptomatic, rapidly progressive, required urgent intervention, occurred with a decline in performance status, or confirmation of progression at 4 to 6 weeks with repeat imaging or for up to 24 months without disease progression. Assessment of tumor status was performed every 9 weeks. The main efficacy outcome measures were OS and PFS as assessed by BICR according to RECIST v1.1, modified to follow a maximum of 10 target lesions and a maximum of 5 target lesions per organ, in the subgroup of patients with TPS ≥50% and the overall population with TPS ≥1%. Additional efficacy outcome measures were ORR and DoR in the subgroup of patients with TPS ≥50% and the overall population with TPS ≥1%.

The study population characteristics were: median age of 63 years (range: 20 to 88), 42% age 65 or older; 61% male; 72% White and 21% Asian; 66% ECOG PS of 1; 43% with high PD-L1 tumor expression; 21% with squamous, 70% with nonsquamous, and 8% with mixed, other or unknown histology; 91% metastatic (M1) disease; 15% with history of brain metastases; and 8% and 1% with EGFR and ALK genomic aberrations, respectively. All patients had received prior therapy with a platinum-doublet regimen, 29% received two or more prior therapies for their metastatic disease.

Tables 69 and 70 and Figure 9 summarize efficacy results in the subgroup with TPS ≥50% population and in all patients, respectively.

Table 69: Efficacy Results of the Subgroup of Patients with TPS ≥50% in KEYNOTE-010
Endpoint | KEYTRUDA 2 mg/kg every 3 weeks n=139 | KEYTRUDA 10 mg/kg every 3 weeks n=151 | Docetaxel 75 mg/m^2 every 3 weeks n=152
OS
Deaths (%) | 58 (42%) | 60 (40%) | 86 (57%)
Median in months (95% CI) | 14.9 (10.4, NR) | 17.3 (11.8, NR) | 8.2 (6.4, 10.7)
Hazard ratio [Hazard ratio (KEYTRUDA compared to docetaxel) based on the stratified Cox proportional hazard model] (95% CI) | 0.54 (0.38, 0.77) | 0.50 (0.36, 0.70) | ---
p-Value (stratified log-rank) | <0.001 | <0.001 | ---
PFS
Events (%) | 89 (64%) | 97 (64%) | 118 (78%)
Median in months (95% CI) | 5.2 (4.0, 6.5) | 5.2 (4.1, 8.1) | 4.1 (3.6, 4.3)
Hazard ratio (95% CI) | 0.58 (0.43, 0.77) | 0.59 (0.45, 0.78) | ---
p-Value (stratified log-rank) | <0.001 | <0.001 | ---
Objective Response Rate
ORR [All responses were partial responses] (95% CI) | 30% (23, 39) | 29% (22, 37) | 8% (4, 13)
p-Value (Miettinen-Nurminen) | <0.001 | <0.001 | ---
Median duration of response in months (range) | NR (0.7+, 16.8+) | NR (2.1+, 17.8+) | 8.1 (2.1+, 8.8+)
NR = not reached

Table 70: Efficacy Results of All Randomized Patients (TPS ≥1%) in KEYNOTE-010
Endpoint | KEYTRUDA 2 mg/kg every 3 weeks n=344 | KEYTRUDA 10 mg/kg every 3 weeks n=346 | Docetaxel 75 mg/m^2 every 3 weeks n=343
OS
Deaths (%) | 172 (50%) | 156 (45%) | 193 (56%)
Median in months (95% CI) | 10.4 (9.4, 11.9) | 12.7 (10.0, 17.3) | 8.5 (7.5, 9.8)
Hazard ratio [Hazard ratio (KEYTRUDA compared to docetaxel) based on the stratified Cox proportional hazard model] (95% CI) | 0.71 (0.58, 0.88) | 0.61 (0.49, 0.75) | ---
p-Value (stratified log-rank) | <0.001 | <0.001 | ---
PFS
Events (%) | 266 (77%) | 255 (74%) | 257 (75%)
Median in months (95% CI) | 3.9 (3.1, 4.1) | 4.0 (2.6, 4.3) | 4.0 (3.1, 4.2)
Hazard ratio (95% CI) | 0.88 (0.73, 1.04) | 0.79 (0.66, 0.94) | ---
p-Value (stratified log-rank) | 0.068 | 0.005 | ---
Objective Response Rate
ORR [All responses were partial responses] (95% CI) | 18% (14, 23) | 19% (15, 23) | 9% (7, 13)
p-Value (Miettinen-Nurminen) | <0.001 | <0.001 | ---
Median duration of response in months (range) | NR (0.7+, 20.1+) | NR (2.1+, 17.8+) | 6.2 (1.4+, 8.8+)
NR = not reached

Figure 9: Kaplan-Meier Curve for Overall Survival in all Randomized Patients in KEYNOTE-010 (TPS ≥1%)

Neoadjuvant and adjuvant treatment of resectable NSCLC

The efficacy of KEYTRUDA in combination with neoadjuvant chemotherapy followed by surgery and continued adjuvant treatment with KEYTRUDA as a single agent was investigated in KEYNOTE-671 (NCT03425643), a multicenter, randomized, double-blind, placebo-controlled trial conducted in 797 patients with previously untreated and resectable Stage II, IIIA, or IIIB (N2) NSCLC by AJCC 8th edition. Patients were enrolled regardless of tumor PD-L1 expression. Patients with active autoimmune disease that required systemic therapy within 2 years of treatment, a medical condition that required immunosuppression, or a history of interstitial lung disease or pneumonitis that required steroids were ineligible. Randomization was stratified by stage (II vs. III), tumor PD-L1 expression (TPS ≥50% or <50%), histology (squamous vs. nonsquamous), and geographic region (East Asia vs. non-East Asia).

Patients were randomized (1:1) to one of the following treatment arms:

- Treatment Arm A: neoadjuvant KEYTRUDA 200 mg on Day 1 in combination with cisplatin 75 mg/m^2 and either pemetrexed 500 mg/m^2 on Day 1 or gemcitabine 1000 mg/m^2 on Days 1 and 8 of each 21-day cycle for up to 4 cycles. Within 4-12 weeks following surgery, KEYTRUDA 200 mg was administered every 3 weeks for up to 13 cycles.
- Treatment Arm B: neoadjuvant placebo on Day 1 in combination with cisplatin 75 mg/m^2 and either pemetrexed 500 mg/m^2 on Day 1 or gemcitabine 1000 mg/m^2 on Days 1 and 8 of each 21-day cycle for up to 4 cycles. Within 4-12 weeks following surgery, placebo was administered every 3 weeks for up to 13 cycles.

All study medications were administered via intravenous infusion. Treatment with KEYTRUDA or placebo continued until completion of the treatment (17 cycles), disease progression that precluded definitive surgery, disease recurrence in the adjuvant phase, disease progression for those who did not undergo surgery or had incomplete resection and entered the adjuvant phase, or unacceptable toxicity. Assessment of tumor status was performed at baseline, Week 7, and Week 13 in the neoadjuvant phase and within 4 weeks prior to the start of the adjuvant phase. Following the start of the adjuvant phase, assessment of tumor status was performed every 16 weeks through the end of Year 3, and then every 6 months thereafter.

The trial was not designed to isolate the effect of KEYTRUDA in each phase (neoadjuvant or adjuvant) of treatment.

The major efficacy outcome measures were OS and investigator-assessed event-free survival (EFS). Additional efficacy outcome measures were pathological complete response (pCR) rate and major pathological response (mPR) rate as assessed by blinded independent pathology review.

The study population characteristics were: median age of 64 years (range: 26 to 83); 45% age 65 or older and 7% age 75 or older; 71% male; 61% White, 31% Asian, 2% Black, 4% race not reported; 9% Hispanic or Latino; 63% ECOG PS of 0 and 37% ECOG PS of 1. Thirty percent had Stage II and 70% had Stage III disease; 33% had TPS ≥50% and 67% had TPS <50%; 43% had tumors with squamous histology and 57% had tumors with non-squamous histology; 31% were from the East Asian region.

Eighty-one percent of patients in the KEYTRUDA in combination with platinum-containing chemotherapy arm received definitive surgery compared to 76% of patients in the placebo in combination with platinum-containing chemotherapy arm.

The trial demonstrated statistically significant improvements in OS and EFS for patients randomized to KEYTRUDA in combination with platinum-containing chemotherapy followed by KEYTRUDA as a single agent compared with patients randomized to placebo in combination with platinum-containing chemotherapy followed by placebo alone.

Table 71 and Figure 10 summarize the efficacy results for KEYNOTE-671.

Table 71: Efficacy Results in KEYNOTE-671
Endpoint | KEYTRUDA 200 mg every 3 weeks with chemotherapy/KEYTRUDA n=397 | Placebo with chemotherapy/Placebo n=400
OS
Number of patients with event (%) | 110 (28%) | 144 (36%)
Median in months [Based on Kaplan-Meier estimates] (95% CI) | NR (NR, NR) | 52.4 (45.7, NR)
Hazard ratio [Based on Cox regression model with treatment as a covariate stratified by stage, tumor PD-L1 expression, histology, and geographic region] (95% CI) | 0.72 (0.56, 0.93)
p-Value [Based on stratified log-rank test] , [Compared to a two-sided p-Value boundary of 0.0109] | 0.0103
EFS
Number of patients with event (%) | 139 (35%) | 205 (51%)
Median in months (95% CI) | NR (34.1, NR) | 17.0 (14.3, 22.0)
Hazard ratio (95% CI) | 0.58 (0.46, 0.72)
p-Value, [Compared to a two-sided p-Value boundary of 0.0092] | <0.0001
NR = not reached

Figure 10: Kaplan-Meier Curve for Overall Survival in KEYNOTE-671

The trial demonstrated a statistically significant difference in pCR rate (18.1% vs. 4.0%; p<0.0001) and mPR rate (30.2% vs. 11.0%; p<0.0001).

Adjuvant treatment of resected NSCLC

The efficacy of KEYTRUDA was investigated in KEYNOTE-091 (NCT02504372), a multicenter, randomized, triple-blind, placebo-controlled trial conducted in 1177 patients with completely resected Stage IB (T2a ≥4 cm), II, or IIIA NSCLC by AJCC 7th edition. Patients had not received neoadjuvant radiotherapy or chemotherapy. Adjuvant chemotherapy up to 4 cycles was optional. Patients were ineligible if they had active autoimmune disease, were on chronic immunosuppressive agents, or had a history of interstitial lung disease or pneumonitis. Randomization was stratified by stage (IB vs. II vs. IIIA), receipt of adjuvant chemotherapy (yes vs. no), PD-L1 status (TPS <1% [negative] vs. TPS 1-49% vs. TPS ≥50%), and geographic region (Western Europe vs. Eastern Europe vs. Asia vs. Rest of World). Patients were randomized (1:1) to receive KEYTRUDA 200 mg or placebo intravenously every 3 weeks.

Treatment continued until RECIST v1.1-defined disease recurrence as determined by the investigator, unacceptable toxicity or up to one year. Tumor assessments were conducted every 12 weeks for the first year, then every 6 months for years 2 to 3, and then annually through year 5. After year 5, imaging was performed as per local standard of care. The major efficacy outcome measure was investigator-assessed disease-free survival (DFS). An additional efficacy outcome measure was OS.

Of 1177 patients randomized, 1010 (86%) received adjuvant platinum-based chemotherapy following resection. Among these 1010 patients, the median age was 64 years (range: 35 to 84), 49% age 65 or older; 68% male; 77% White, 18% Asian; 86% current or former smokers; and 39% with ECOG PS of 1. Eleven percent had Stage IB, 57% had Stage II, and 31% had Stage IIIA disease. Thirty-nine percent had PD-L1 TPS <1% [negative], 33% had TPS 1-49%, and 28% had TPS ≥50%. Fifty-two percent were from Western Europe, 20% from Eastern Europe, 17% from Asia, and 11% from Rest of World.

The trial met its primary endpoint, demonstrating a statistically significant improvement in DFS in the overall population for patients randomized to the KEYTRUDA arm compared to patients randomized to the placebo arm. In an exploratory subgroup analysis of the 167 patients (14%) who did not receive adjuvant chemotherapy, the DFS HR was 1.25 (95% CI: 0.76, 2.05). OS results were not mature with only 42% of pre-specified OS events in the overall population.

Table 72 and Figure 11 summarize the efficacy results for KEYNOTE-091 in patients who received adjuvant chemotherapy.

Table 72: Efficacy Results in KEYNOTE-091 for Patients Who Received Adjuvant Chemotherapy
Endpoint | KEYTRUDA 200 mg every 3 weeks n=506 | Placebo n=504
DFS
Number (%) of patients with event | 177 (35%) | 231 (46%)
Median in months (95% CI) | 58.7 (39.2, NR) | 34.9 (28.6, NR)
Hazard ratio [Based on the unstratified univariate Cox regression model] (95% CI) | 0.73 (0.60, 0.89)
NR = not reached

Figure 11: Kaplan-Meier Curve for Disease-Free Survival in KEYNOTE-091 for Patients Who Received Adjuvant Chemotherapy

14.3 Malignant Pleural Mesothelioma

First-line treatment of unresectable advanced or metastatic malignant pleural mesothelioma (MPM) with pemetrexed and platinum chemotherapy

The efficacy of KEYTRUDA in combination with pemetrexed and platinum chemotherapy was investigated in KEYNOTE-483 (NCT02784171), a multicenter, randomized, open-label, active-controlled trial that enrolled 440 patients with unresectable advanced or metastatic MPM and no prior systemic therapy for advanced/metastatic disease. Patients were enrolled regardless of tumor PD-L1 expression. Patients with autoimmune disease that required systemic therapy within 3 years of treatment or a medical condition that required immunosuppression were ineligible. Randomization was stratified by histological subtype (epithelioid vs. non-epithelioid). Patients were randomized (1:1) to one of the following treatment arms; all study medications were administered via intravenous infusion:

- KEYTRUDA 200 mg with pemetrexed 500 mg/m^2 and cisplatin 75 mg/m^2 or carboplatin AUC 5-6 mg/mL/min on Day 1 of each 21-day cycle for up to 6 cycles, followed by KEYTRUDA 200 mg every 3 weeks. KEYTRUDA was administered prior to chemotherapy on Day 1.
- Pemetrexed 500 mg/m^2 and cisplatin 75 mg/m^2 or carboplatin AUC 5-6 mg/mL/min on Day 1 of each 21-day cycle for up to 6 cycles.

Treatment with KEYTRUDA continued until disease progression as determined by the investigator according to modified RECIST 1.1 for mesothelioma (mRECIST), unacceptable toxicity, or a maximum of 24 months. Assessment of tumor status was performed every 6 weeks for 18 weeks, followed by every 12 weeks thereafter. The main efficacy outcome measure was OS. Additional efficacy outcome measures were PFS, ORR, and DoR, as assessed by BICR according to mRECIST.

The study population characteristics were: median age of 70 years (77% age 65 or older); 76% male; 79% White, 21% race not reported or unknown; 2% Hispanic or Latino; and 53% ECOG performance status of 1. Seventy-eight percent had epithelioid and 22% had non-epithelioid histology; 60% had tumors with PD-L1 CPS ≥1 and 30% had tumors with PD-L1 CPS <1.

The trial demonstrated a statistically significant improvement in OS, PFS, and ORR in patients randomized to KEYTRUDA in combination with chemotherapy compared with patients randomized to chemotherapy alone. Table 73 and Figure 12 summarize the efficacy results for KEYNOTE-483.

Table 73: Efficacy Results in KEYNOTE-483
Endpoint | KEYTRUDA 200 mg every 3 weeks Pemetrexed Platinum Chemotherapy | Pemetrexed Platinum Chemotherapy
 | (n=222) | (n=218)
OS
Number (%) of patients with event | 167 (75%) | 175 (80%)
Median in months (95% CI) | 17.3 (14.4, 21.3) | 16.1 (13.1, 18.2)
Hazard ratio [Based on stratified Cox proportional hazard model] (95% CI) | 0.79 (0.64, 0.98)
p-Value [Based on stratified log-rank test] | 0.0162
PFS
Number (%) of patients with event | 190 (86%) | 166 (76%)
Median in months (95% CI) | 7.1 (6.9, 8.1) | 7.1 (6.8, 7.7)
Hazard ratio (95% CI) | 0.80 (0.65, 0.99)
p-Value | 0.0194
Objective Response Rate
ORR % (95% CI) | 52% (45.5, 59.0) | 29% (23.0, 35.4)
Complete responses | 1 (0.5%) | 0 (0%)
Partial responses | 115 (52%) | 63 (29%)
p-Value [Based on Miettinen and Nurminen method stratified by histological subtype at randomization (epithelioid vs. non-epithelioid)] | <0.00001
Duration of Response [Based on patients with a best overall response as confirmed complete or partial response; n=116 for patients in the KEYTRUDA combination arm; n=63 for patients in the chemotherapy arm]
Median in months (95% CI) | 6.9 (5.8, 8.3) | 6.8 (5.5, 8.5)

Figure 12: Kaplan-Meier Curve for Overall Survival in KEYNOTE-483

In a pre-specified exploratory analysis based on histology, in the subgroup of patients with epithelioid histology (n=345), the hazard ratio (HR) for OS was 0.89 (95% CI: 0.70, 1.13), with median OS of 19.8 months in KEYTRUDA in combination with chemotherapy and 18.2 months in chemotherapy alone. In the subgroup of patients with non-epithelioid histology (n=95), the HR for OS was 0.57 (95% CI: 0.36, 0.89), with median OS of 12.3 months in KEYTRUDA in combination with chemotherapy and 8.2 months in chemotherapy alone.

14.4 Head and Neck Squamous Cell Cancer

Neoadjuvant and Adjuvant Treatment of Locally Advanced HNSCC for Tumors Expressing PD-L1 (CPS≥ 1)

The efficacy of KEYTRUDA was investigated in KEYNOTE-689 (NCT02358031), a randomized, multicenter, open-label, active-controlled trial conducted in 714 patients with resectable locally advanced (Stage III-IVA) HNSCC [AJCC, 8th edition]. Patients with active autoimmune disease requiring systemic therapy within two years of treatment or a medical condition that required immunosuppression were ineligible. Randomization was stratified by primary tumor site (oropharynx/oral cavity vs. larynx vs. hypopharynx), tumor stage (III vs. IVA) and PD-L1 status (TPS ≥ 50% vs. TPS<50%) according to the PD-L1 IHC 22C3 pharmDx assay.

Patients were randomized (1:1) to one of the following treatment arms:

- neoadjuvant KEYTRUDA 200 mg for 2 cycles prior to surgical resection. Within 6 weeks following surgery, 3 cycles of adjuvant KEYTRUDA 200 mg every 3 weeks in combination with radiotherapy (RT) with or without 3 cycles of cisplatin 100 mg/m^2 every 3 weeks. This was followed by KEYTRUDA 200 mg every 3 weeks for up to 12 cycles.
- no neoadjuvant treatment prior to surgery. Within 6 weeks following surgery, adjuvant RT with or without 3 cycles of concurrent cisplatin 100 mg/m^2 every 3 weeks.
  On both treatment arms, patients received cisplatin with adjuvant RT if high-risk pathological features (i.e., positive margins <1 mm or extranodal extension) were present at surgery.

Treatment with KEYTRUDA continued until disease progression by RECIST v1.1 per BICR during the neoadjuvant phase that precluded surgery, local or metastatic recurrence during the adjuvant phase, completion of treatment, or unacceptable toxicity. Assessment of tumor status was performed prior to surgery at Week 6 in the neoadjuvant phase. Following the start of the adjuvant phase, assessment of tumor status was performed 12 weeks after end of RT with or without cisplatin treatment and then every 3 months until the end of year 3; then every 6 months thereafter up to the end of year 5.

The trial was not designed to isolate the effect of KEYTRUDA in each phase (neoadjuvant or adjuvant) of treatment.

The major efficacy outcome measure was event-free survival (EFS) by BICR defined as the time from randomization to the first occurrence of any of the following events: progression of disease that precludes definitive surgery, local or distant disease progression or recurrence, or death due to any cause. Additional efficacy outcome measures were major pathological response (mPR) as assessed by BIPR, and overall survival (OS).

The demographic and baseline characteristics in the 682 patients with PD-L1 expression of CPS ≥1 were: median age of 60 years (range: 22 to 87), 33% age 65 or older; 79% male; 78% White, 13% Asian and 2.5% Black or African American, 14% were Hispanic or Latino; 43% had ECOG PS of 1, and 79% were former/current smokers. Four percent of patients’ tumors were HPV-positive, and 26% had Stage III disease, 74% had Stage IVA disease. Sixty-eight percent of patients’ tumors had PD-L1 expression of CPS ≥10.

Eighty-eight percent of patients received definitive surgery in both the KEYTRUDA and the SOC arm.

Seventy-six percent of patients in the KEYTRUDA arm and 78% of patients in the SOC arm started the radiation phase of treatment. In the KEYTRUDA arm, 35% of patients received KEYTRUDA and cisplatin with concurrent RT, 57% of patients received KEYTRUDA alone with concurrent RT, 3% of patients received cisplatin alone with concurrent RT, 5% of patients received RT alone and one patient (0.4%) received KEYTRUDA alone without concurrent RT. On the SoC arm, 52% of patients received cisplatin with concurrent RT while 48% patients received RT alone.

The trial demonstrated a statistically significant improvement in EFS for patients randomized to the KEYTRUDA arm compared to those randomized to the standard of care (SOC) arm at the first pre-specified interim analysis. Table 74 and Figure 13 summarize efficacy results in KEYNOTE-689 for patients with HNSCC CPS ≥1.

Table 74: Efficacy Results for Perioperative KEYTRUDA with adjuvant RT with or without cisplatin in Patients with HNSCC CPS ≥1 in KEYNOTE-689
Endpoint | KEYTRUDA 200 mg every 3 weeks with RT with or without cisplatin n=347 | RT with or without cisplatin n=335
EFS
Number of events, n (%) | 128 (37%) | 156 (47%)
Median in months [From product-limit (Kaplan-Meier) method for censored data.] (95% CI) | 59.7 (37.9, NR) | 29.6 (19.5, 41.9)
Hazard ratio [Based on Cox regression model with Efron’s method of tie handling with treatment as a covariate stratified by primary tumor site and tumor stage.] (95% CI) | 0.70 (0.55, 0.89)
p-Value [One-sided p-value based on log-rank test stratified by primary tumor site and tumor stage. Compared to a one-sided p-value boundary of 0.0124] , | 0.00140
NR = not reached

Figure 13: Kaplan-Meier Curve for Event-free Survival for KEYTRUDA in Patients with HNSCC CPS ≥1 in KEYNOTE-689

While OS results were not mature at this interim analysis, with 76% of pre-specified OS events in the CPS≥1 population, no trend towards a detriment was observed.

Hypopharyngeal Tumors

In an exploratory subgroup analysis of patients with PD-L1-positive (CPS ≥1) hypopharyngeal tumors who were randomized (n=51), the EFS HR was 2.28 (95% CI: 0.79, 6.56). Among these patients, 23 patients in the KEYTRUDA arm received surgery, of which 17 patients (74%) had R0 resections. On the SOC arm, 23 patients received surgery, of which 20 (87%) had R0 resections.

Oral Cavity, Oropharyngeal and Laryngeal Tumors

In an exploratory subgroup analysis of patients with PD-L1 positive (CPS ≥1) oral cavity, oropharyngeal and laryngeal tumors who received surgery (n=555), 91% of patients on the KEYTRUDA arm had R0 resections while 85% of patients on the SOC arm had R0 resections.

First-line treatment of metastatic or unresectable, recurrent HNSCC

The efficacy of KEYTRUDA was investigated in KEYNOTE-048 (NCT02358031), a randomized, multicenter, open-label, active-controlled trial conducted in 882 patients with metastatic HNSCC who had not previously received systemic therapy for metastatic disease or with recurrent disease who were considered incurable by local therapies. Patients with active autoimmune disease that required systemic therapy within two years of treatment or a medical condition that required immunosuppression were ineligible. Randomization was stratified by tumor PD-L1 expression (TPS ≥50% or <50%) according to the PD-L1 IHC 22C3 pharmDx assay, HPV status according to p16 IHC (positive or negative), and ECOG PS (0 vs. 1). Patients were randomized 1:1:1 to one of the following treatment arms:

- KEYTRUDA 200 mg intravenously every 3 weeks
- KEYTRUDA 200 mg intravenously every 3 weeks, carboplatin AUC 5 mg/mL/min intravenously every 3 weeks or cisplatin 100 mg/m^2 intravenously every 3 weeks, and FU 1000 mg/m^2/day as a continuous intravenous infusion over 96 hours every 3 weeks (maximum of 6 cycles of platinum and FU)
- Cetuximab 400 mg/m^2 intravenously as the initial dose then 250 mg/m^2 intravenously once weekly, carboplatin AUC 5 mg/mL/min intravenously every 3 weeks or cisplatin 100 mg/m^2 intravenously every 3 weeks, and FU 1000 mg/m^2/day as a continuous intravenous infusion over 96 hours every 3 weeks (maximum of 6 cycles of platinum and FU)

Treatment with KEYTRUDA continued until RECIST v1.1-defined progression of disease as determined by the investigator, unacceptable toxicity, or a maximum of 24 months. Administration of KEYTRUDA was permitted beyond RECIST-defined disease progression if the patient was clinically stable and considered to be deriving clinical benefit by the investigator. Assessment of tumor status was performed at Week 9 and then every 6 weeks for the first year, followed by every 9 weeks through 24 months. A retrospective re-classification of patients' tumor PD-L1 status according to CPS using the PD-L1 IHC 22C3 pharmDx assay was conducted using the tumor specimens used for randomization.

The main efficacy outcome measures were OS and PFS as assessed by BICR according to RECIST v1.1 (modified to follow a maximum of 10 target lesions and a maximum of 5 target lesions per organ) sequentially tested in the subgroup of patients with CPS ≥20, the subgroup of patients with CPS ≥1, and the overall population.

The study population characteristics were: median age of 61 years (range: 20 to 94), 36% age 65 or older; 83% male; 73% White, 20% Asian and 2.4% Black; 61% had ECOG PS of 1; and 79% were former/current smokers. Twenty-two percent of patients' tumors were HPV-positive, 23% had PD-L1 TPS ≥50%, and 95% had Stage IV disease (Stage IVA 19%, Stage IVB 6%, and Stage IVC 70%). Eighty-five percent of patients' tumors had PD-L1 expression of CPS ≥1 and 43% had CPS ≥20.

The trial demonstrated a statistically significant improvement in OS for patients randomized to KEYTRUDA in combination with chemotherapy compared to those randomized to cetuximab in combination with chemotherapy at a pre-specified interim analysis in the overall population. Table 75 and Figure 14 summarize efficacy results for KEYTRUDA in combination with chemotherapy.

Table 75: Efficacy Results [Results at a pre-specified interim analysis] for KEYTRUDA plus Platinum/Fluorouracil in KEYNOTE-048
Endpoint | KEYTRUDA 200 mg every 3 weeks Platinum FU | Cetuximab Platinum FU
 | n=281 | n=278
OS
Number (%) of patients with event | 197 (70%) | 223 (80%)
Median in months (95% CI) | 13.0 (10.9, 14.7) | 10.7 (9.3, 11.7)
Hazard ratio [Based on the stratified Cox proportional hazard model] (95% CI) | 0.77 (0.63, 0.93)
p-Value [Based on stratified log-rank test] | 0.0067
PFS
Number of patients with event (%) | 244 (87%) | 253 (91%)
Median in months (95% CI) | 4.9 (4.7, 6.0) | 5.1 (4.9, 6.0)
Hazard ratio (95% CI) | 0.92 (0.77, 1.10)
p-Value | 0.3394
Objective Response Rate
ORR [Response: Best objective response as confirmed complete response or partial response] (95% CI) | 36% (30.0, 41.5) | 36% (30.7, 42.3)
Complete response rate | 6% | 3%
Partial response rate | 30% | 33%
Duration of Response
Median in months (range) | 6.7 (1.6+, 30.4+) | 4.3 (1.2+, 27.9+)

At the pre-specified final OS analysis for the ITT population, the hazard ratio was 0.72 (95% CI: 0.60, 0.87). In addition, KEYNOTE-048 demonstrated a statistically significant improvement in OS for the subgroups of patients with PD-L1 CPS ≥1 (HR=0.65, 95% CI: 0.53, 0.80) and CPS ≥20 (HR=0.60, 95% CI: 0.45, 0.82).

Figure 14: Kaplan-Meier Curve for Overall Survival for KEYTRUDA plus Platinum/Fluorouracil in KEYNOTE-048 [At the time of the protocol-specified final analysis.]

First-line treatment of metastatic or unresectable, recurrent HNSCC for Tumors Expressing PD-L1 (CPS≥ 1) as a single agent

The trial also demonstrated a statistically significant improvement in OS for the subgroup of patients with PD-L1 CPS ≥1 randomized to KEYTRUDA as a single agent compared to those randomized to cetuximab in combination with chemotherapy at a pre-specified interim analysis. At the time of the interim and final analyses, there was no significant difference in OS between the KEYTRUDA single agent arm and the control arm for the overall population.

Table 76 summarizes efficacy results for KEYTRUDA as a single agent in the subgroups of patients with CPS ≥1 HNSCC and CPS ≥20 HNSCC. Figure 15 summarizes the OS results in the subgroup of patients with CPS ≥1 HNSCC.

Table 76: Efficacy Results [Results at a pre-specified interim analysis] for KEYTRUDA as a Single Agent in KEYNOTE-048 (CPS ≥1 and CPS ≥20)
Endpoint | CPS ≥1 |  | CPS ≥20
Endpoint | KEYTRUDA 200 mg every 3 weeks | Cetuximab Platinum FU | KEYTRUDA 200 mg every 3 weeks | Cetuximab Platinum FU
Endpoint | n=257 | n=255 | n=133 | n=122
OS
Number of events (%) | 177 (69%) | 206 (81%) | 82 (62%) | 95 (78%)
Median in months (95% CI) | 12.3 (10.8, 14.9) | 10.3 (9.0, 11.5) | 14.9 (11.6, 21.5) | 10.7 (8.8, 12.8)
Hazard ratio [Based on the stratified Cox proportional hazard model] (95% CI) | 0.78 (0.64, 0.96) |  | 0.61 (0.45, 0.83)
p-Value [Based on a stratified log-rank test] | 0.0171 |  | 0.0015
PFS
Number of events (%) | 225 (88%) | 231 (91%) | 113 (85%) | 111 (91%)
Median in months (95% CI) | 3.2 (2.2, 3.4) | 5.0 (4.8, 5.8) | 3.4 (3.2, 3.8) | 5.0 (4.8, 6.2)
Hazard ratio (95% CI) | 1.15 (0.95, 1.38) |  | 0.97 (0.74, 1.27)
Objective Response Rate
ORR [Response: Best objective response as confirmed complete response or partial response] (95% CI) | 19% (14.5, 24.4) | 35% (29.1, 41.1) | 23% (16.4, 31.4) | 36% (27.6, 45.3)
Complete response rate | 5% | 3% | 8% | 3%
Partial response rate | 14% | 32% | 16% | 33%
Duration of Response
Median in months (range) | 20.9 (1.5+, 34.8+) | 4.5 (1.2+, 28.6+) | 20.9 (2.7, 34.8+) | 4.2 (1.2+, 22.3+)

At the pre-specified final OS analysis comparing KEYTRUDA as a single agent to cetuximab in combination with chemotherapy, the hazard ratio for the subgroup of patients with CPS ≥1 was 0.74 (95% CI: 0.61, 0.90) and the hazard ratio for the subgroup of patients with CPS ≥20 was 0.58 (95% CI: 0.44, 0.78).

In an exploratory subgroup analysis for patients with CPS 1-19 HNSCC at the time of the pre-specified final OS analysis, the median OS was 10.8 months (95% CI: 9.0, 12.6) for KEYTRUDA as a single agent and 10.1 months (95% CI: 8.7, 12.1) for cetuximab in combination with chemotherapy, with an HR of 0.86 (95% CI: 0.66, 1.12).

Figure 15: Kaplan-Meier Curve for Overall Survival for KEYTRUDA as a Single Agent in KEYNOTE-048 (CPS ≥1) [At the time of the protocol-specified final analysis.]

Previously treated recurrent or metastatic HNSCC

The efficacy of KEYTRUDA was investigated in KEYNOTE-012 (NCT01848834), a multicenter, non-randomized, open-label, multi-cohort study that enrolled 174 patients with recurrent or metastatic HNSCC who had disease progression on or after platinum-containing chemotherapy administered for recurrent or metastatic HNSCC or following platinum-containing chemotherapy administered as part of induction, concurrent, or adjuvant therapy. Patients with active autoimmune disease, a medical condition that required immunosuppression, evidence of interstitial lung disease, or ECOG PS ≥2 were ineligible.

Patients received KEYTRUDA 10 mg/kg every 2 weeks (n=53) or 200 mg every 3 weeks (n=121) until unacceptable toxicity or disease progression that was symptomatic, was rapidly progressive, required urgent intervention, occurred with a decline in performance status, or was confirmed at least 4 weeks later with repeat imaging. Patients without disease progression were treated for up to 24 months. Treatment with pembrolizumab could be reinitiated for subsequent disease progression and administered for up to 1 additional year. Assessment of tumor status was performed every 8 weeks. The major efficacy outcome measures were ORR according to RECIST v1.1, modified to follow a maximum of 10 target lesions and a maximum of 5 target lesions per organ, as assessed by BICR, and DoR.

The study population characteristics were median age of 60 years, 32% age 65 or older; 82% male; 75% White, 16% Asian, and 6% Black; 87% had M1 disease; 33% had HPV positive tumors; 63% had prior cetuximab; 29% had an ECOG PS of 0 and 71% had an ECOG PS of 1; and the median number of prior lines of therapy administered for the treatment of HNSCC was 2.

The ORR was 16% (95% CI: 11, 22) with a complete response rate of 5%. The median follow-up time was 8.9 months. Among the 28 responding patients, the median DoR had not been reached (range: 2.4+ to 27.7+ months), with 23 patients having responses of 6 months or longer. The ORR and DoR were similar irrespective of dosage regimen (10 mg/kg every 2 weeks or 200 mg every 3 weeks) or HPV status.

14.5 Classical Hodgkin Lymphoma

KEYNOTE-204

The efficacy of KEYTRUDA was investigated in KEYNOTE-204 (NCT02684292), a randomized, open-label, active controlled trial conducted in 304 patients with relapsed or refractory cHL. The trial enrolled adults with relapsed or refractory disease after at least one multi-agent chemotherapy regimen. Patients were randomized (1:1) to receive:

- KEYTRUDA 200 mg intravenously every 3 weeks or
- Brentuximab vedotin (BV) 1.8 mg/kg intravenously every 3 weeks

Treatment was continued until unacceptable toxicity, disease progression, or a maximum of 35 cycles (up to approximately 2 years). Disease assessment was performed every 12 weeks. Randomization was stratified by prior autologous HSCT (yes vs. no) and disease status after frontline therapy (primary refractory vs. relapse <12 months after completion vs. relapse ≥12 months after completion). The main efficacy measure was PFS as assessed by BICR using 2007 revised International Working Group criteria.

The study population characteristics were: median age of 35 years (range: 18 to 84); 57% male; 77% White, 9% Asian, 3.9% Black. The median number of prior therapies was 2 (range: 1 to 10) in the KEYTRUDA arm and 3 (range: 1 to 11) in the BV arm, with 18% in both arms having 1 prior line. Forty-two percent of patients were refractory to the last prior therapy, 29% had primary refractory disease, 37% had prior autologous HSCT, 5% had received prior BV, and 39% had prior radiation therapy.

Efficacy is summarized in Table 77 and Figure 16.

Table 77: Efficacy Results in Patients with cHL in KEYNOTE-204
Endpoint | KEYTRUDA 200 mg every 3 weeks n=151 | Brentuximab Vedotin 1.8 mg/kg every 3 weeks n=153
PFS
Number of patients with event (%) | 81 (54%) | 88 (58%)
Median in months (95% CI) [Based on Kaplan-Meier estimates.] | 13.2 (10.9, 19.4) | 8.3 (5.7, 8.8)
Hazard ratio [Based on the stratified Cox proportional hazard model.] (95% CI) | 0.65 (0.48, 0.88)
p-Value [Based on a stratified log-rank test. One-sided p-Value, with a prespecified boundary of 0.0043.] | 0.0027
Objective Response Rate
ORR [Difference in ORR is not statistically significant.] (95% CI) | 66% (57, 73) | 54% (46, 62)
Complete response | 25% | 24%
Partial response | 41% | 30%
Duration of Response
Median in months (range) | 20.7 (0.0+, 33.2+) | 13.8 (0.0+, 33.9+)
+ Denotes a censored value.

Figure 16: Kaplan-Meier Curve for Progression-Free Survival in KEYNOTE-204

KEYNOTE-087

The efficacy of KEYTRUDA was investigated in KEYNOTE-087 (NCT02453594), a multicenter, non-randomized, open-label trial in 210 patients with relapsed or refractory cHL. Patients with active, non-infectious pneumonitis, an allogeneic HSCT within the past 5 years (or >5 years but with symptoms of GVHD), active autoimmune disease, a medical condition that required immunosuppression, or an active infection requiring systemic therapy were ineligible for the trial. Patients received KEYTRUDA 200 mg intravenously every 3 weeks until unacceptable toxicity or documented disease progression, or for up to 24 months in patients who did not progress. Disease assessment was performed every 12 weeks. The major efficacy outcome measures (ORR, Complete Response Rate, and DoR) were assessed by BICR according to the 2007 revised International Working Group (IWG) criteria.

The study population characteristics were: median age of 35 years (range: 18 to 76), 9% age 65 or older; 54% male; 88% White; and 49% ECOG PS of 0 and 51% ECOG PS of 1. The median number of prior lines of therapy administered for the treatment of cHL was 4 (range: 1 to 12). Fifty-eight percent were refractory to the last prior therapy, including 35% with primary refractory disease and 14% whose disease was chemo-refractory to all prior regimens. Sixty-one percent of patients had undergone prior autologous HSCT, 83% had received prior brentuximab vedotin and 36% of patients had prior radiation therapy.

Efficacy results for KEYNOTE-087 are summarized in Table 78.

Table 78: Efficacy Results in Patients with cHL in KEYNOTE-087
Endpoint | KEYTRUDA 200 mg every 3 weeks n=210 [Median follow-up time of 9.4 months]
Objective Response Rate
ORR (95% CI) | 69% (62, 75)
Complete response rate | 22%
Partial response rate | 47%
Duration of Response
Median in months (range) | 11.1 (0.0+, 11.1) [Based on patients (n=145) with a response by independent review]

14.6 Primary Mediastinal Large B-Cell Lymphoma

The efficacy of KEYTRUDA was investigated in KEYNOTE-170 (NCT02576990), a multicenter, open-label, single-arm trial in 53 patients with relapsed or refractory PMBCL. Patients were not eligible if they had active non-infectious pneumonitis, allogeneic HSCT within the past 5 years (or >5 years but with symptoms of GVHD), active autoimmune disease, a medical condition that required immunosuppression, or an active infection requiring systemic therapy. Patients were treated with KEYTRUDA 200 mg intravenously every 3 weeks until unacceptable toxicity or documented disease progression, or for up to 24 months for patients who did not progress. Disease assessments were performed every 12 weeks and assessed by BICR according to the 2007 revised IWG criteria. The efficacy outcome measures were ORR and DoR.

The study population characteristics were: median age of 33 years (range: 20 to 61 years); 43% male; 92% White; and 43% ECOG PS of 0 and 57% ECOG PS of 1. The median number of prior lines of therapy administered for the treatment of PMBCL was 3 (range 2 to 8). Thirty-six percent had primary refractory disease, 49% had relapsed disease refractory to the last prior therapy, and 15% had untreated relapse. Twenty-six percent of patients had undergone prior autologous HSCT, and 32% of patients had prior radiation therapy. All patients had received rituximab as part of a prior line of therapy.

For the 24 responders, the median time to first objective response (complete or partial response) was 2.8 months (range 2.1 to 8.5 months). Efficacy results for KEYNOTE-170 are summarized in Table 79.

Table 79: Efficacy Results in Patients with PMBCL in KEYNOTE-170
Endpoint | KEYTRUDA 200 mg every 3 weeks n=53 [Median follow-up time of 9.7 months]
Objective Response Rate
ORR (95% CI) | 45% (32, 60)
Complete response rate | 11%
Partial response rate | 34%
Duration of Response
Median in months (range) | NR (1.1+, 19.2+) [Based on patients (n=24) with a response by independent review]
NR = not reached

14.7 Urothelial Cancer

In Combination with Enfortumab Vedotin for the Treatment of Patients with Urothelial Cancer

The efficacy of KEYTRUDA in combination with enfortumab vedotin was evaluated in KEYNOTE-A39 (NCT04223856), an open-label, randomized, multicenter trial that enrolled 886 patients with locally advanced or metastatic urothelial cancer who received no prior systemic therapy for locally advanced or metastatic disease. Patients with active CNS metastases, ongoing sensory or motor neuropathy Grade ≥2, or uncontrolled diabetes defined as hemoglobin A1C (HbA1c) ≥8% or HbA1c ≥7% with associated diabetes symptoms were excluded.

Patients were randomized 1:1 to receive either:

- KEYTRUDA 200 mg over 30 minutes on Day 1 and enfortumab vedotin 1.25 mg/kg on Days 1 and 8 of each 21-day cycle. KEYTRUDA was given approximately 30 minutes after enfortumab vedotin. Treatment was continued until disease progression or unacceptable toxicity. In the absence of disease progression or unacceptable toxicity, KEYTRUDA was continued for up to 2 years.
- Gemcitabine 1000 mg/m^2 on Days 1 and 8 of a 21-day cycle with cisplatin 70 mg/m^2 or carboplatin (AUC = 4.5 or 5) on Day 1 of a 21-day cycle. Treatment was continued until disease progression or unacceptable toxicity for up to 6 cycles.

Randomization was stratified by cisplatin eligibility, PD-L1 expression, and presence of liver metastases.

The median age was 69 years (range: 22 to 91); 77% were male; 67% were White, 22% were Asian, 1% were Black or African American, and 10% were unknown or other; 12% were Hispanic or Latino. Patients had a baseline ECOG performance status of 0 (49%), 1 (47%), or 2 (3%). Forty-seven percent of patients had a documented baseline HbA1c of <5.7%. At baseline, 95% of patients had metastatic urothelial cancer, including 72% with visceral and 22% with liver metastases, and 5% had locally advanced urothelial cancer. Eighty-five percent of patients had urothelial carcinoma (UC) histology including 6% with UC mixed squamous differentiation and 2% with UC mixed other histologic variants. Forty-six percent of patients were considered cisplatin-ineligible and 54% were considered cisplatin-eligible at time of randomization.

The major efficacy outcome measures were OS and PFS as assessed by BICR according to RECIST v1.1. Additional efficacy outcome measures included ORR as assessed by BICR.

The trial demonstrated statistically significant improvements in OS, PFS, and ORR for patients randomized to KEYTRUDA in combination with enfortumab vedotin as compared to platinum-based chemotherapy. Efficacy results were consistent across all stratified patient subgroups.

Table 80 and Figures 17 and 18 summarize the efficacy results for KEYNOTE-A39.

Table 80: Efficacy Results in KEYNOTE-A39
Endpoint | KEYTRUDA 200 mg every 3 weeks in combination with Enfortumab Vedotin n=442 | Cisplatin or carboplatin with gemcitabine n=444
OS
Number (%) of patients with event | 133 (30%) | 226 (51%)
Median in months (95% CI) | 31.5 (25.4, NR) | 16.1 (13.9, 18.3)
Hazard ratio [Based on the stratified Cox proportional hazard regression model] (95% CI) | 0.47 (0.38, 0.58)
p-Value [Two-sided p-Value based on stratified log-rank test] | <0.0001
PFS
Number (%) of patients with event | 223 (50%) | 307 (69%)
Median in months (95% CI) | 12.5 (10.4, 16.6) | 6.3 (6.2, 6.5)
Hazard ratio (95% CI) | 0.45 (0.38, 0.54)
p-Value | <0.0001
Confirmed Objective Response Rate [Includes only patients with measurable disease at baseline (n=437 for KEYTRUDA in combination with enfortumab vedotin, n=441 for chemotherapy).]
ORR [Based on patients with a best overall response as confirmed complete or partial response] % (95% CI) | 68% (63, 72) | 44% (40, 49)
p-Value [Two-sided p-Value based on Cochran-Mantel-Haenszel test stratified by PD-L1 expression, cisplatin eligibility and liver metastases] | <0.0001
Complete response | 29% | 12%
Partial response | 39% | 32%
NR = not reached

Figure 17: Kaplan-Meier Curve for Overall Survival in KEYNOTE-A39

Figure 18: Kaplan-Meier Curve for Progression-Free Survival in KEYNOTE-A39

In Combination with Enfortumab Vedotin for the Treatment of Cisplatin-Ineligible Patients with Urothelial Cancer

The efficacy of KEYTRUDA in combination with enfortumab vedotin was evaluated in KEYNOTE-869 (NCT03288545), an open-label, multi-cohort (dose escalation cohort, Cohort A, Cohort K) study in patients with locally advanced or metastatic urothelial cancer who were ineligible for cisplatin-containing chemotherapy and received no prior systemic therapy for locally advanced or metastatic disease. Patients with active CNS metastases, ongoing sensory or motor neuropathy Grade ≥2, or uncontrolled diabetes defined as hemoglobin A1C (HbA1c) ≥8% or HbA1c ≥7% with associated diabetes symptoms were excluded from participating in the study.

Patients in the dose escalation cohort (n=5), Cohort A (n=40), and Cohort K (n=76) received enfortumab vedotin 1.25 mg/kg as an IV infusion over 30 minutes on Days 1 and 8 of a 21-day cycle followed by KEYTRUDA 200 mg as an IV infusion on Day 1 of a 21-day cycle approximately 30 minutes after enfortumab vedotin. Patients were treated until disease progression or unacceptable toxicity.

A total of 121 patients received KEYTRUDA in combination with enfortumab vedotin. The median age was 71 years (range: 51 to 91); 74% were male; 85% were White, 5% were Black, 4% were Asian and 6% were other, unknown or not reported. Ten percent of patients were Hispanic or Latino. Forty-five percent of patients had an ECOG performance status of 1 and 15% had an ECOG performance status of 2. Forty-seven percent of patients had a documented baseline HbA1c of <5.7%. Reasons for cisplatin-ineligibility included: 60% with baseline creatinine clearance of 30-59 mL/min, 10% with ECOG PS of 2, 13% with Grade 2 or greater hearing loss, and 16% with more than one cisplatin-ineligibility criteria.

At baseline, 97.5% of patients had metastatic urothelial cancer and 2.5% of patients had locally advanced urothelial cancer. Thirty-seven percent of patients had upper tract disease. Eighty-four percent of patients had visceral metastasis at baseline, including 22% with liver metastases. Thirty-nine percent of patients had TCC histology; 13% had TCC with squamous differentiation, and 48% had TCC with other histologic variants.

The major efficacy outcome measures were ORR and DoR as assessed by BICR according to RECIST v1.1.

The median follow-up time for the dose escalation cohort + Cohort A was 44.7 months (range 0.7 to 52.4) and for Cohort K was 14.8 months (range: 0.6 to 26.2).

Efficacy results are presented in Table 81 below.

Table 81: Efficacy Results in KEYNOTE-869, Combined Dose Escalation Cohort, Cohort A, and Cohort K
Endpoint | KEYTRUDA in combination with Enfortumab Vedotin n=121
Confirmed ORR (95% CI) | 68% (58.7, 76.0)
Complete response rate | 12%
Partial response rate | 55%

The median duration of response for the dose escalation cohort + Cohort A was 22.1 months (range: 1.0+ to 46.3+) and for Cohort K was not reached (range: 1.2 to 24.1+).

Platinum-Ineligible Patients with Urothelial Carcinoma

The efficacy of KEYTRUDA was investigated in KEYNOTE-052 (NCT02335424), a multicenter, open-label, single-arm trial in 370 patients with locally advanced or metastatic urothelial carcinoma who had one or more comorbidities, including patients who were not eligible for any platinum-containing chemotherapy. The trial excluded patients with autoimmune disease or a medical condition that required immunosuppression. Patients received KEYTRUDA 200 mg every 3 weeks until unacceptable toxicity or disease progression. Patients with initial radiographic disease progression could receive additional doses of treatment during confirmation of progression unless disease progression was symptomatic, was rapidly progressive, required urgent intervention, or occurred with a decline in performance status. Patients without disease progression could be treated for up to 24 months. Tumor response assessments were performed at 9 weeks after the first dose, then every 6 weeks for the first year, and then every 12 weeks thereafter. The major efficacy outcome measures were ORR and DoR as assessed by BICR according to RECIST v1.1, modified to follow a maximum of 10 target lesions and a maximum of 5 target lesions per organ.

The study population characteristics were: median age of 74 years; 77% male; and 89% White. Eighty-seven percent had M1 disease, and 13% had M0 disease. Eighty-one percent had a primary tumor in the lower tract, and 19% of patients had a primary tumor in the upper tract. Eighty-five percent of patients had visceral metastases, including 21% with liver metastases. Fifty percent of patients had baseline creatinine clearance of <60 mL/min, 32% had ECOG PS of 2, 9% had ECOG PS of 2 and baseline creatinine clearance of <60 mL/min, and 9% had one or more of Class III heart failure, Grade 2 or greater peripheral neuropathy, and Grade 2 or greater hearing loss. Ninety percent of patients were treatment naïve, and 10% received prior adjuvant or neoadjuvant platinum-based chemotherapy.

The median follow-up time for 370 patients treated with KEYTRUDA was 11.4 months (range 0.1 to 63.8 months). Efficacy results are summarized in Table 82.

Table 82: Efficacy Results in KEYNOTE-052
Endpoint | KEYTRUDA 200 mg every 3 weeks
 | All Subjects n=370
Objective Response Rate
ORR (95% CI) | 29% (24, 34)
Complete response rate | 10%
Partial response rate | 20%
Duration of Response
Median in months (range) | 33.4 (1.4+, 60.7+)
+ Denotes ongoing response

Platinum-Eligible Patients with Previously Untreated Urothelial Carcinoma

The efficacy of KEYTRUDA for the first-line treatment of platinum-eligible patients with locally advanced or metastatic urothelial carcinoma was investigated in KEYNOTE-361 (NCT02853305), a multicenter, randomized, open-label, active-controlled study in 1010 previously untreated patients. The safety and efficacy of KEYTRUDA in combination with platinum-based chemotherapy for previously untreated patients with locally advanced or metastatic urothelial carcinoma has not been established.

The study compared KEYTRUDA with or without platinum-based chemotherapy (i.e., cisplatin or carboplatin with gemcitabine) to platinum-based chemotherapy alone. Among the patients receiving KEYTRUDA plus platinum-based chemotherapy, 44% received cisplatin and 56% received carboplatin.

The study did not meet its major efficacy outcome measures of improved PFS or OS in the KEYTRUDA plus chemotherapy arm compared to the chemotherapy-alone arm. Additional efficacy endpoints, including improvement of OS in the KEYTRUDA monotherapy arm, could not be formally tested.

Previously Treated Urothelial Carcinoma

The efficacy of KEYTRUDA was investigated in KEYNOTE-045 (NCT02256436), a multicenter, randomized (1:1), active-controlled trial in 542 patients with locally advanced or metastatic urothelial carcinoma with disease progression on or after platinum-containing chemotherapy. The trial excluded patients with autoimmune disease or a medical condition that required immunosuppression.

Patients were randomized to receive either KEYTRUDA 200 mg every 3 weeks (n=270) or investigator's choice of any of the following chemotherapy regimens all given intravenously every 3 weeks (n=272): paclitaxel 175 mg/m^2 (n=90), docetaxel 75 mg/m^2 (n=92), or vinflunine 320 mg/m^2 (n=90). Treatment continued until unacceptable toxicity or disease progression. Patients with initial radiographic disease progression could receive additional doses of treatment during confirmation of progression unless disease progression was symptomatic, was rapidly progressive, required urgent intervention, or occurred with a decline in performance status. Patients without disease progression could be treated for up to 24 months. Assessment of tumor status was performed at 9 weeks after randomization, then every 6 weeks through the first year, followed by every 12 weeks thereafter. The major efficacy outcomes were OS and PFS as assessed by BICR per RECIST v1.1, modified to follow a maximum of 10 target lesions and a maximum of 5 target lesions per organ. Additional efficacy outcome measures were ORR as assessed by BICR per RECIST v1.1, modified to follow a maximum of 10 target lesions and a maximum of 5 target lesions per organ, and DoR.

The study population characteristics were: median age of 66 years (range: 26 to 88), 58% age 65 or older; 74% male; 72% White and 23% Asian; 42% ECOG PS of 0 and 56% ECOG PS of 1; and 96% M1 disease and 4% M0 disease. Eighty-seven percent of patients had visceral metastases, including 34% with liver metastases. Eighty-six percent had a primary tumor in the lower tract and 14% had a primary tumor in the upper tract. Fifteen percent of patients had disease progression following prior platinum-containing neoadjuvant or adjuvant chemotherapy. Twenty-one percent had received 2 or more prior systemic regimens in the metastatic setting. Seventy-six percent of patients received prior cisplatin, 23% had prior carboplatin, and 1% were treated with other platinum-based regimens.

The study demonstrated statistically significant improvements in OS and ORR for patients randomized to KEYTRUDA as compared to chemotherapy. There was no statistically significant difference between KEYTRUDA and chemotherapy with respect to PFS. The median follow-up time for this trial was 9.0 months (range: 0.2 to 20.8 months). Table 83 and Figure 19 summarize the efficacy results for KEYNOTE-045.

Table 83: Efficacy Results in KEYNOTE-045
 | KEYTRUDA 200 mg every 3 weeks | Chemotherapy
 | n=270 | n=272
OS
Deaths (%) | 155 (57%) | 179 (66%)
Median in months (95% CI) | 10.3 (8.0, 11.8) | 7.4 (6.1, 8.3)
Hazard ratio [Hazard ratio (KEYTRUDA compared to chemotherapy) based on the stratified Cox proportional hazard model] (95% CI) | 0.73 (0.59, 0.91)
p-Value (stratified log-rank) | 0.004
PFS by BICR
Events (%) | 218 (81%) | 219 (81%)
Median in months (95% CI) | 2.1 (2.0, 2.2) | 3.3 (2.3, 3.5)
Hazard ratio (95% CI) | 0.98 (0.81, 1.19)
p-Value (stratified log-rank) | 0.833
Objective Response Rate
ORR (95% CI) | 21% (16, 27) | 11% (8, 16)
Complete response rate | 7% | 3%
Partial response rate | 14% | 8%
p-Value (Miettinen-Nurminen) | 0.002
Median duration of response in months (range) | NR (1.6+, 15.6+) | 4.3 (1.4+, 15.4+)
+ Denotes ongoing response
NR = not reached

Figure 19: Kaplan-Meier Curve for Overall Survival in KEYNOTE-045

Neoadjuvant and Adjuvant Treatment of Cisplatin-Ineligible Patients with MIBC in Combination with Enfortumab Vedotin

The efficacy of KEYTRUDA in combination with enfortumab vedotin as neoadjuvant treatment and continued after radical cystectomy as adjuvant treatment was investigated in KEYNOTE-905 (NCT03924895), an open-label, randomized, multicenter, active-controlled trial in patients with previously untreated MIBC with predominant urothelial carcinoma histology and who were candidates for radical cystectomy (RC) with pelvic lymph node dissection (PLND) but were ineligible for or declined cisplatin-based chemotherapy. The study excluded patients with primary non-bladder urothelial cancer (i.e., cancer of the ureter, urethra, or renal pelvis) and those with active autoimmune disease that required systemic therapy within 2 years of treatment or a medical condition that required immunosuppression.

Randomization was stratified by tumor stage (T2N0 vs T3/T4aN0 vs T1-T4aN1), cisplatin-eligibility (cisplatin-ineligible vs cisplatin-eligible but declined), and geographic region (United States vs European Union vs Rest of World).

Patients were randomized 1:1 to receive:

- Neoadjuvant KEYTRUDA 200 mg over 30 minutes as an intravenous infusion on Day 1 and enfortumab vedotin 1.25 mg/kg as an intravenous infusion on Days 1 and 8 of each 21-day cycle for 3 cycles prior to surgery, followed by adjuvant KEYTRUDA 200 mg over 30 minutes on Day 1 of each 21-day cycle for 14 cycles and adjuvant enfortumab vedotin 1.25 mg/kg on Days 1 and 8 of each 21-day cycle for 6 cycles (n=170).
- Immediate RC and PLND alone (n=174).

Treatment continued until completion of study medications, disease progression, not undergoing or refusal of RC and PLND, disease recurrence in the adjuvant phase, or unacceptable toxicity. Assessment of tumor status, including CT/MRI, was performed at baseline, within 5 weeks prior to RC and PLND, and at 6 weeks post-radical cystectomy. Following RC and PLND, assessment of tumor status, including cystoscopy and urine cytology for patients who did not undergo surgery, was performed every 12 weeks up to 2 years, and every 24 weeks thereafter.

The study population characteristics were: median age of 73 years (range: 46 to 87 years); 78% male; 78% White, 16% Asian, 3.2% Multiple, 1.2% Black or African American, 0.3% American Indian or Alaska Native, and 1.2% missing; 6% Hispanic or Latino, 91% not Hispanic or Latino, and 2.9% not reported; 57% had ECOG PS of 0, 29% had ECOG PS of 1, and 14% had ECOG PS of 2; 18% were T2N0, 77% T3/T4aN0, and 4.9% T1-T4aN1. Ninety-one percent of patients had pure urothelial carcinoma histology; 4.4% had urothelial carcinoma with squamous differentiation, 2.6% had urothelial carcinoma with glandular differentiation, and 2% had urothelial carcinoma with other variant histology. Among the 281 patients who were ineligible for cisplatin, 72% had baseline creatinine clearance of 30-59 mL/min, 17% had ECOG PS of 2, 21% had Grade 2 or greater hearing loss, 3.9% had New York Heart Association Class III heart failure, and 13% met more than one cisplatin-ineligibility criterion.

A total of 149 (88%) patients in the KEYTRUDA in combination with enfortumab vedotin arm and 156 (90%) patients in the RC and PLND alone arm underwent RC and PLND.

The trial was not designed to isolate the effect of KEYTRUDA in each phase (neoadjuvant or adjuvant) of treatment.

The major efficacy outcome measure was EFS as assessed by BICR. Overall survival (OS) and pathological complete response (pCR) rate as assessed by blinded independent pathology review were additional efficacy outcome measures.

The trial demonstrated a statistically significant improvement in EFS and OS in patients treated with neoadjuvant and adjuvant KEYTRUDA in combination with enfortumab vedotin compared with RC and PLND alone. Table 84 and Figures 20 and 21 summarize key efficacy measures.

Table 84: Efficacy Results for Perioperative KEYTRUDA with Enfortumab Vedotin in KEYNOTE-905
Endpoint | KEYTRUDA 200 mg every 3 weeks in combination with enfortumab vedotin before and after RC with PLND n=170 | RC with PLND alone n=174
EFS
Number of patients with event (%) | 48 (28%) | 95 (55%)
Median in months [Based on Kaplan-Meier estimates] (95% CI) | NR (37.3, NR) | 15.7 (10.3, 20.5)
Hazard ratio [Based on stratified Cox regression model with Efron’s method of tie handling with treatment as a covariate] (95% CI) | 0.40 (0.28, 0.57)
p-Value [Based on stratified log-rank test] | <0.0001
OS
Number of patients with event (%) | 38 (22%) | 68 (39%)
Median in months (95% CI) | NR (NR, NR) | 41.7 (31.8, NR)
Hazard ratio (95% CI) | 0.50 (0.33, 0.74)
p-Value | 0.0002
NR = not reached
EFS is defined as time from randomization to the first of: disease progression preventing curative surgery, failure to undergo surgery for participants with muscle invasive residual disease, incomplete surgical resection, local or distant recurrence after surgery, or death.

Figure 20: Kaplan-Meier Curve for Event-Free Survival by Treatment Arm in KEYNOTE-905

Figure 21: Kaplan-Meier Curve for Overall Survival by Treatment Arm in KEYNOTE-905

The trial demonstrated a statistically significant difference in pCR rate (57.1% [95% CI: 49.3, 64.6] vs. 8.6% [95% CI: 4.9, 13.8]; p<0.0001).

BCG-unresponsive High-Risk Non-Muscle Invasive Bladder Cancer

The efficacy of KEYTRUDA was investigated in KEYNOTE-057 (NCT02625961), a multicenter, open-label, single-arm trial in 96 patients with Bacillus Calmette-Guerin (BCG)-unresponsive, high-risk, non-muscle invasive bladder cancer (NMIBC) with carcinoma in situ (CIS) with or without papillary tumors who are ineligible for or have elected not to undergo cystectomy. BCG-unresponsive high-risk NMIBC was defined as persistent disease despite adequate BCG therapy, disease recurrence after an initial tumor-free state following adequate BCG therapy, or T1 disease following a single induction course of BCG. Adequate BCG therapy was defined as administration of at least five of six doses of an initial induction course plus either of: at least two of three doses of maintenance therapy or at least two of six doses of a second induction course. Prior to treatment, all patients had undergone transurethral resection of bladder tumor (TURBT) to remove all resectable disease (Ta and T1 components). Residual CIS (Tis components) not amenable to complete resection was allowed. The trial excluded patients with muscle invasive (i.e., T2, T3, T4) locally advanced non-resectable or metastatic urothelial carcinoma, concurrent extra-vesical (i.e., urethra, ureter or renal pelvis) non-muscle invasive transitional cell carcinoma of the urothelium, or autoimmune disease or a medical condition that required immunosuppression.

Patients received KEYTRUDA 200 mg every 3 weeks until unacceptable toxicity, persistent or recurrent high-risk NMIBC, or progressive disease. Assessment of tumor status was performed every 12 weeks for two years and then every 24 weeks for three years, and patients without disease progression could be treated for up to 24 months. The major efficacy outcome measures were complete response (as defined by negative results for cystoscopy [with TURBT/biopsies as applicable], urine cytology, and computed tomography urography [CTU] imaging) and duration of response.

The study population characteristics were: median age of 73 years (range: 44 to 92); 44% age ≥75; 84% male; 67% White; and 73% and 27% with an ECOG performance status of 0 or 1, respectively. Tumor pattern at study entry was CIS with T1 (13%), CIS with high grade TA (25%), and CIS (63%). Baseline high-risk NMIBC disease status was 27% persistent and 73% recurrent. The median number of prior instillations of BCG was 12.

The median follow-up time was 28.0 months (range: 4.6 to 40.5 months). Efficacy results are summarized in Table 85.

Table 85: Efficacy Results in KEYNOTE-057
Endpoint | KEYTRUDA 200 mg every 3 weeks n=96
Complete Response Rate (95% CI) | 41% (31, 51)
Duration of Response [Based on patients (n=39) that achieved a complete response; reflects period from the time complete response was achieved]
Median in months (range) | 16.2 (0.0+, 30.4 [Denotes ongoing response])
% (n) with duration ≥12 months | 46% (18)

14.8 Microsatellite Instability-High or Mismatch Repair Deficient Cancer

The efficacy of KEYTRUDA was investigated in 504 patients with MSI-H or dMMR cancers enrolled in three multicenter, non-randomized, open-label, multi-cohort trials: KEYNOTE-164 (NCT02460198), KEYNOTE-158 (NCT02628067), and KEYNOTE-051 (NCT02332668). All trials excluded patients with autoimmune disease or a medical condition that required immunosuppression. Regardless of histology, MSI or MMR tumor status was determined using polymerase chain reaction (PCR; local or central) or immunohistochemistry (IHC; local or central), respectively.

- KEYNOTE-164 enrolled 124 patients with advanced MSI-H or dMMR colorectal cancer (CRC) that progressed following treatment with fluoropyrimidine and either oxaliplatin or irinotecan +/- anti-VEGF/EGFR mAb-based therapy.
- KEYNOTE-158 enrolled 373 patients with advanced MSI-H or dMMR non-colorectal cancers (non-CRC) who had disease progression following prior therapy. Patients were either prospectively enrolled with MSI-H/dMMR tumors (Cohort K) or retrospectively identified in one of 10 solid tumor cohorts (Cohorts A-J).
- KEYNOTE-051 enrolled 7 pediatric patients with MSI-H or dMMR cancers.

Adult patients received KEYTRUDA 200 mg every 3 weeks (pediatric patients received 2 mg/kg every 3 weeks) until unacceptable toxicity, disease progression, or a maximum of 24 months. In KEYNOTE-164 and KEYNOTE-158, assessment of tumor status was performed every 9 weeks through the first year, then every 12 weeks thereafter. In KEYNOTE-051, assessment of tumor status was performed every 8 weeks for 24 weeks, and then every 12 weeks thereafter. The major efficacy outcome measures were ORR and DoR as assessed by BICR according to RECIST v1.1 (modified to follow a maximum of 10 target lesions and a maximum of 5 target lesions per organ in KEYNOTE-158) and as assessed by the investigator according to RECIST v1.1 in KEYNOTE-051.

In KEYNOTE-164 and KEYNOTE-158, the study population characteristics were median age of 60 years, 36% age 65 or older; 44% male; 78% White, 14% Asian, 4% American Indian or Alaska Native, and 3% Black; and 45% ECOG PS of 0 and 55% ECOG PS of 1. Ninety-two percent of patients had metastatic disease and 4% had locally advanced, unresectable disease. Thirty-seven percent of patients received one prior line of therapy and 61% received two or more prior lines of therapy.

In KEYNOTE-051, the study population characteristics were median age of 11 years (range: 3 to 16); 71% female; 86% White and 14% Asian; and 57% had a Lansky/Karnofsky Score of 100. Seventy-one percent of patients had Stage IV and 14% had Stage III disease. Fifty-seven percent of patients received one prior line of therapy and 29% received two prior lines of therapy.

Discordant results were observed between local MSI-H or dMMR tests and central testing among patients enrolled in Cohort K of KEYNOTE-158. Among 104 tumor samples that were MSI-H or dMMR by local testing and also tested using the FoundationOne®CDx (F1CDx) test, 59 (56.7%) were MSI-H and 45 (43.3%) were not MSI-H. Among 169 tumor samples that were MSI-H or dMMR by local testing and also tested using the VENTANA MMR RxDx Panel, 105 (62.1%) were dMMR and 64 (37.9%) were pMMR.

Efficacy results are summarized in Tables 86 and 87.

Table 86: Efficacy Results for Patients with MSI-H/dMMR Cancer
Endpoint | KEYTRUDA n=504 [Median follow-up time of 20.1 months (range 0.1 to 71.4 months)]
Objective Response Rate
ORR (95% CI) [Of the 7 pediatric patients from KEYNOTE-051, 1 patient had a radiographic complete response after initial growth of their tumor but is not reflected in the results.] | 33.3% (29.2, 37.6)
Complete response rate | 10.3%
Partial response rate | 23.0%
Duration of Response | n=168
Median in months (range) | 63.2 (1.9+, 63.9+)
% with duration ≥12 months | 77%
% with duration ≥36 months | 39%
+ Denotes ongoing response

Table 87: Response by Tumor Type
 |  | Objective Response Rate |  | Duration of Response range
 | N | n (%) | 95% CI | (months)
CRC | 124 | 42 (34%) | (26%, 43%) | (4.4, 58.5+)
Non-CRC [Results include patients in Cohort K of KEYNOTE-158 that were later determined to be pMMR or not MSI-H by central testing] | 380 | 126 (33%) | (28%, 38%) | (1.9+, 63.9+)
Endometrial cancer | 94 | 47 (50%) | (40%, 61%) | (2.9, 63.2)
Gastric or GE junction cancer | 51 | 20 (39%) | (26%, 54%) | (1.9+, 63.0+)
Small intestinal cancer | 27 | 16 (59%) | (39%, 78%) | (3.7+, 57.3+)
Brain cancer | 27 [Includes 6 pediatric patients with brain cancer] | 1 (4%) [In addition to the 1 adult responder, 1 pediatric patient had a radiographic complete response after initial growth of their tumor.] | (0%, 19%) | 18.9
Ovarian cancer | 25 | 8 (32%) | (15%, 54%) | (4.2, 56.6+)
Biliary cancer | 22 | 9 (41%) | (21%, 64%) | (6.2, 49.0+)
Pancreatic cancer | 22 | 4 (18%) | (5%, 40%) | (8.1, 24.3+)
Sarcoma | 14 | 3 (21%) | (5%, 51%) | (35.4+, 57.2+)
Breast cancer | 13 | 1 (8%) | (0%,36%) | 24.3+
Other [Includes tumor type (n): anal (3), HNSCC (1), nasopharyngeal (1), retroperitoneal (1), testicular (1), vaginal (1), vulvar (1), appendiceal adenocarcinoma, NOS (1), hepatocellular carcinoma (1), and carcinoma of unknown origin (1). Includes 1 pediatric patient with abdominal adenocarcinoma.] | 13 | 4 (31%) | (9%, 61%) | (6.2+, 32.3+)
Cervical cancer | 11 | 1 (9%) | (0%, 41%) | 63.9+
Neuroendocrine cancer | 11 | 1 (9%) | (0%, 41%) | 13.3
Prostate cancer | 8 | 1 (13%) | (0%, 53%) | 24.5+
Adrenocortical cancer | 7 | 1 (14%) | (0%, 58%) | 4.2
Mesothelioma | 7 | 0 (0%) | (0%, 41%)
Thyroid cancer | 7 | 1 (14%) | (0%, 58%) | 8.2
Small cell lung cancer | 6 | 2 (33%) | (4%, 78%) | (20.0, 47.5)
Bladder cancer | 6 | 3 (50%) | (12%, 88%) | (35.6+, 57.5+)
Salivary cancer | 5 | 2 (40%) | (5%, 85%) | (42.6+, 57.8+)
Renal cell cancer | 4 | 1 (25%) | (0%, 81%) | 22.0
+ Denotes ongoing response

Exploratory analysis by TMB

In an exploratory analysis performed in 138 patients (Cohort K of KEYNOTE-158) who were tested retrospectively for tumor mutation burden (TMB) using an FDA-authorized test, 45 (33%) had tumors with TMB score of <10 mut/Mb; ORR in these 45 patients was 6.7% (95% CI: 1.4, 18.3). Among the 45 patients with TMB score of <10 mut/Mb, 39 of the patients were pMMR/not MSI-H when tested using an FDA-authorized test.

14.9 Microsatellite Instability-High or Mismatch Repair Deficient Colorectal Cancer

The efficacy of KEYTRUDA was investigated in KEYNOTE-177 (NCT02563002), a multicenter, randomized, open-label, active-controlled trial that enrolled 307 patients with previously untreated unresectable or metastatic MSI-H or dMMR CRC. MSI or MMR tumor status was determined locally using polymerase chain reaction (PCR) or immunohistochemistry (IHC), respectively. Patients with autoimmune disease or a medical condition that required immunosuppression were ineligible.

Patients were randomized (1:1) to receive KEYTRUDA 200 mg intravenously every 3 weeks or investigator’s choice of the following chemotherapy regimens given intravenously every 2 weeks:

- mFOLFOX6 (oxaliplatin, leucovorin, and FU) or mFOLFOX6 in combination with either bevacizumab or cetuximab: Oxaliplatin 85 mg/m^2, leucovorin 400 mg/m^2 (or levoleucovorin 200 mg/m^2), and FU 400 mg/m^2 bolus on Day 1, then FU 2400 mg/m^2 over 46-48 hours. Bevacizumab 5 mg/kg on Day 1 or cetuximab 400 mg/m^2 on first infusion, then 250 mg/m^2 weekly.
- FOLFIRI (irinotecan, leucovorin, and FU) or FOLFIRI in combination with either bevacizumab or cetuximab: Irinotecan 180 mg/m^2, leucovorin 400 mg/m^2 (or levoleucovorin 200 mg/m^2), and FU 400 mg/m^2 bolus on Day 1, then FU 2400 mg/m^2 over 46-48 hours. Bevacizumab 5 mg/kg on Day 1 or cetuximab 400 mg/m^2 on first infusion, then 250 mg/m^2 weekly.

Treatment with KEYTRUDA or chemotherapy continued until RECIST v1.1-defined progression of disease as determined by the investigator or unacceptable toxicity. Patients treated with KEYTRUDA without disease progression could be treated for up to 24 months. Assessment of tumor status was performed every 9 weeks. Patients randomized to chemotherapy were offered KEYTRUDA at the time of disease progression. The main efficacy outcome measures were PFS (as assessed by BICR according to RECIST v1.1, modified to follow a maximum of 10 target lesions and a maximum of 5 target lesions per organ) and OS. Additional efficacy outcome measures were ORR and DoR.

A total of 307 patients were enrolled and randomized to KEYTRUDA (n=153) or chemotherapy (n=154). The baseline characteristics of these 307 patients were: median age of 63 years (range: 24 to 93), 47% age 65 or older; 50% male; 75% White and 16% Asian; 52% had an ECOG PS of 0 and 48% had an ECOG PS of 1; and 27% received prior adjuvant or neoadjuvant chemotherapy. Among 154 patients randomized to receive chemotherapy,143 received chemotherapy per the protocol. Of the 143 patients, 56% received mFOLFOX6, 44% received FOLFIRI, 70% received bevacizumab plus mFOLFOX6 or FOLFIRI, and 11% received cetuximab plus mFOLFOX6 or FOLFIRI.

The trial demonstrated a statistically significant improvement in PFS for patients randomized to KEYTRUDA compared with chemotherapy. There was no statistically significant difference between KEYTRUDA and chemotherapy in the final OS analysis. Sixty percent of the patients who had been randomized to receive chemotherapy had crossed over to receive subsequent anti-PD-1/PD-L1 therapies including KEYTRUDA. The median follow-up time at the final analysis was 38.1 months (range: 0.2 to 58.7 months). Table 88 and Figure 22 summarize the key efficacy measures for KEYNOTE-177.

Table 88: Efficacy Results in Patients with MSI-H or dMMR CRC in KEYNOTE-177
Endpoint | KEYTRUDA 200 mg every 3 weeks n=153 | Chemotherapy n=154
PFS
Number (%) of patients with event | 82 (54%) | 113 (73%)
Median in months (95% CI) | 16.5 (5.4, 32.4) | 8.2 (6.1, 10.2)
Hazard ratio [Based on Cox regression model] (95% CI) | 0.60 (0.45, 0.80)
p-Value [Two-sided p-Value based on log-rank test (compared to a significance level of 0.0234)] | 0.0004
OS [Final OS analysis]
Number (%) of patients with event | 62 (41%) | 78 (51%)
Median in months (95% CI) | NR (49.2, NR) | 36.7 (27.6, NR)
Hazard ratio (95% CI) | 0.74 (0.53, 1.03)
p-Value [Two-sided p-Value based on log-rank test (compared to a significance level of 0.0492)] | 0.0718
Objective Response Rate [Based on confirmed response by BICR review]
ORR (95% CI) | 44% (35.8, 52.0) | 33% (25.8, 41.1)
Complete response rate | 11% | 4%
Partial response rate | 33% | 29%
Duration of Response, [Based on n=67 patients with a response in the KEYTRUDA arm and n=51 patients with a response in the chemotherapy arm]
Median in months (range) | NR (2.3+, 41.4+) | 10.6 (2.8, 37.5+)
% with duration ≥12 months [Based on observed duration of response] | 75% | 37%
% with duration ≥24 months | 43% | 18%
+ Denotes ongoing response
NR = not reached

Figure 22: Kaplan-Meier Curve for PFS in KEYNOTE-177

14.10 Gastric Cancer

First-line Treatment of Locally Advanced Unresectable or Metastatic HER2-Positive Gastric or Gastroesophageal Junction Adenocarcinoma for Tumors Expressing PD-L1 (CPS≥1)

The efficacy of KEYTRUDA in combination with trastuzumab plus fluoropyrimidine and platinum chemotherapy was investigated in KEYNOTE-811 (NCT03615326), a multicenter, randomized, double-blind, placebo-controlled trial that enrolled 698 patients with HER2-positive advanced gastric or gastroesophageal junction (GEJ) adenocarcinoma who had not previously received systemic therapy for metastatic disease. PD-L1 status was determined using the PD-L1 IHC 22C3 pharmDx assay. Patients with an autoimmune disease that required systemic therapy within 2 years of treatment or a medical condition that required immunosuppression were ineligible. Randomization was stratified by PD-L1 expression (CPS ≥1 or CPS <1), chemotherapy regimen (5-FU plus cisplatin [FP] or capecitabine plus oxaliplatin [CAPOX]), and geographic region (Europe/Israel/North America/Australia, Asia, or Rest of the World). Patients were randomized (1:1) to one of the following treatment arms:

- KEYTRUDA 200 mg, trastuzumab 8 mg/kg on first infusion and 6 mg/kg in subsequent cycles, followed by investigator’s choice of combination chemotherapy of cisplatin 80 mg/m^2 for up to 6 cycles and 5-FU 800 mg/m^2/day for 5 days (FP) or oxaliplatin 130 mg/m^2 up to 6-8 cycles and capecitabine 1000 mg/m^2 bid for 14 days (CAPOX). KEYTRUDA was administered prior to trastuzumab and chemotherapy on Day 1 of each cycle.
- Placebo, trastuzumab 8 mg/kg on first infusion and 6 mg/kg in subsequent cycles, followed by investigator’s choice of combination chemotherapy of cisplatin 80 mg/m^2 for up to 6 cycles and 5-FU 800 mg/m^2/day for 5 days (FP) or oxaliplatin 130 mg/m^2 up to 6-8 cycles and capecitabine 1000 mg/m^2 bid for 14 days (CAPOX).

All study medications, except oral capecitabine, were administered as an intravenous infusion every 3-week cycle. Treatment with KEYTRUDA continued until RECIST v1.1-defined progression of disease as determined by BICR, unacceptable toxicity, or a maximum of 24 months. The major outcome measures assessed were PFS by BICR using RECIST v1.1, modified to follow a maximum of 10 target lesions and a maximum of 5 target lesions per organ, and OS.

Additional outcome measures included ORR and DoR, based on BICR using RECIST 1.1, modified to follow a maximum of 10 target lesions and a maximum of 5 target lesions per organ.

Among the 698 patients, randomized, 594 (85%) had tumors that expressed PD-L1 with a CPS ≥1. PD-L1 status was determined using the PD-L1 IHC 22C3 pharmDx assay. The population characteristics of these 594 patients were: median age of 63 years (range: 19 to 85), 43% age 65 or older; 80% male; 63% White, 33% Asian, and 0.7% Black; 42% ECOG PS of 0 and 58% ECOG PS of 1. Ninety-eight percent of patients had metastatic disease (Stage IV) and 2% had locally advanced unresectable disease. Ninety-five percent (n=562) had tumors that were not MSI-H, 1% (n=8) had tumors that were MSI-H, and in 4% (n=24) the status was not known. Eighty-five percent of patients received CAPOX.

A statistically significant improvement in OS and PFS was demonstrated in patients randomized to KEYTRUDA in combination with trastuzumab and chemotherapy compared with placebo in combination with trastuzumab and chemotherapy; however, an exploratory analysis of OS in the PD-L1 CPS <1 population showed a HR of 1.10 (95% CI: 0.72, 1.68), indicating that the improvement in the ITT population was primarily attributed to the results observed in the subgroup of patients with PD-L1 CPS ≥1.

Efficacy results at the final analysis for the subgroup of patients whose tumors expressed PD-L1 with a CPS ≥1 are summarized in Table 89 and Figure 23.

Table 89: Efficacy Results for KEYNOTE-811 with PD-L1 Expression CPS ≥1
Endpoint | KEYTRUDA 200 mg every 3 weeks Trastuzumab Fluoropyrimidine and Platinum Chemotherapy n=298 | Placebo Trastuzumab Fluoropyrimidine and Platinum Chemotherapy n=296
OS
Number (%) of patients with event | 226 (76%) | 244 (82%)
Median in months [Based on Kaplan-Meier estimation] (95% CI) | 20.1 (17.9, 22.9) | 15.7 (13.5, 18.5)
Hazard ratio [Based on the unstratified Cox proportional hazard model] (95% CI) | 0.79 (0.66, 0.95)
PFS
Number (%) of patients with event | 221 (74%) | 226 (76%)
Median in months (95% CI) | 10.9 (8.5, 12.5) | 7.3 (6.8, 8.4)
Hazard ratio (95% CI) | 0.72 (0.60, 0.87)
Objective Response Rate
ORR [Response: Best objective response as confirmed complete response or partial response] (95% CI) | 73% (68, 78) | 58% (53, 64)
Complete response rate | 17% | 10%
Partial response rate | 56% | 48%
Duration of Response | n=218 | n=173
Median in months (95% CI) | 11.3 (9.9, 13.7) | 9.6 (7.1, 11.2)
Range in months | 1.1+, 60.8+ | 1.4+, 60.5+
+ Denotes ongoing response

Figure 23: Kaplan-Meier Curve for Overall Survival by Treatment Arm in KEYNOTE-811 (CPS ≥1)

First-line Treatment of Locally Unresectable or Metastatic HER2-Negative Gastric or Gastroesophageal Junction Adenocarcinoma for Tumors Expressing PD-L1 (CPS≥ 1)

The efficacy of KEYTRUDA in combination with fluoropyrimidine- and platinum-containing chemotherapy was investigated in KEYNOTE-859 (NCT03675737), a multicenter, randomized, double-blind, placebo-controlled trial that enrolled 1579 patients with HER2-negative advanced gastric or GEJ adenocarcinoma who had not previously received systemic therapy for metastatic disease. Patients with an autoimmune disease that required systemic therapy within 2 years of treatment or a medical condition that required immunosuppression were ineligible. Randomization was stratified by PD-L1 expression (CPS ≥1 or CPS <1), chemotherapy regimen (FP or CAPOX), and geographic region (Europe/Israel/North America/Australia, Asia, or Rest of the World). Patients were randomized (1:1) to one of the following treatment arms; treatment was administered prior to chemotherapy on Day 1 of each cycle:

- KEYTRUDA 200 mg, investigator’s choice of combination chemotherapy of cisplatin 80 mg/m^2 and 5-FU 800 mg/m^2/day for 5 days (FP) or oxaliplatin 130 mg/m^2 and capecitabine 1000 mg/m^2 bid for 14 days (CAPOX).
- Placebo, investigator’s choice of combination chemotherapy of cisplatin 80 mg/m^2 and 5-FU 800 mg/m^2/day for 5 days (FP) or oxaliplatin 130 mg/m^2 and capecitabine 1000 mg/m^2 bid for 14 days (CAPOX).

All study medications, except oral capecitabine, were administered as an intravenous infusion every 3-week cycle. Platinum agents could be administered for 6 or more cycles following local guidelines. Treatment with KEYTRUDA continued until RECIST v1.1-defined progression of disease as determined by BICR, unacceptable toxicity, or a maximum of 24 months. The major efficacy outcome measure was OS. Additional secondary efficacy outcome measures included PFS, ORR, and DoR as assessed by BICR using RECIST v1.1, modified to follow a maximum of 10 target lesions and a maximum of 5 target lesions per organ.

Among 1,579 patients, 1,235 (78%) had tumors expressing PD-L1 CPS ≥ 1. The population characteristics in patients with PD-L1 CPS ≥ 1 expressing tumors were: median age of 62 years (range: 24 to 86), 40% age 65 or older; 70% male and 30% female; 55% White, 33% Asian, 4.6% Multiple, 4.3% American Indian or Alaskan Native, 1.3% Black, and 0.2% Native Hawaiian or other Pacific Islander; 76% Not Hispanic or Latino and 21% Hispanic or Latino; 37% ECOG PS of 0 and 63% ECOG PS of 1. Ninety-six percent of patients had metastatic disease (Stage IV) and 3% had locally advanced unresectable disease. Five percent (n=66) had tumors that were MSI-H. Eighty-six percent of patients received CAPOX.

A statistically significant improvement in OS, PFS, and ORR was demonstrated in patients randomized to KEYTRUDA in combination with chemotherapy compared with placebo in combination with chemotherapy at the time of a pre-specified interim analysis of OS; however, an exploratory analysis of OS in the PD-L1 CPS <1 population showed a HR of 0.92 (95% CI 0.73, 1.17) indicating that the improvement in the ITT population was primarily attributed to the results observed in the subgroup of patients with PD-L1 CPS ≥1. Efficacy results for patients whose tumors expressed PD-L1 CPS ≥1 and CPS ≥10 are summarized in Table 90 and Figures 24 and 25.

Table 90: Efficacy Results [Based on a pre-specified interim analysis] for KEYNOTE-859
Endpoint | KEYTRUDA 200 mg every 3 weeks and FP or CAPOX n=618 | Placebo and FP or CAPOX n=617 | KEYTRUDA 200 mg every 3 weeks and FP or CAPOX n=279 | Placebo and FP or CAPOX n=272
 | CPS ≥1 |  | CPS ≥10
OS
Number (%) of patients with event | 464 (75) | 526 (85) | 188 (67) | 226 (83)
Median in months (95% CI) | 13.0 (11.6, 14.2) | 11.4 (10.5, 12.0) | 15.7 (13.8, 19.3) | 11.8 (10.3, 12.7)
Hazard ratio [Based on the stratified Cox proportional hazard model] (95% CI) | 0.74 (0.65, 0.84) |  | 0.65 (0.53, 0.79)
p-Value (stratified log-rank) [One-sided p-Value based on stratified log-rank test] | <0.0001 |  | <0.0001
PFS
Number (%) of patients with event | 443 (72%) | 483 (78%) | 190 (68) | 210 (77)
Median in months (95% CI) | 6.9 (6.0, 7.2) | 5.6 (5.4, 5.7) | 8.1 (6.8, 8.5) | 5.6 (5.4, 6.7)
Hazard ratio (95% CI) | 0.72 (0.63, 0.82) |  | 0.62 (0.51, 0.76)
p-Value (stratified log-rank) | <0.0001 |  | <0.0001
Objective Response Rate
ORR [Response: Best objective response as confirmed complete response or partial response] (95% CI) | 52% (48, 56) | 43% (39, 47) | 61% (55, 66) | 43% (37, 49)
Complete response rate | 10% | 6% | 13% | 5%
Partial response rate | 42% | 37% | 48% | 38%
p-Value [One-sided p-Value based on stratified Miettinen & Nurminen method] | 0.0004 |  | <0.0001
Duration of Response | n=322 | n=263 | n=169 | n=117
Median in months [Based on Kaplan-Meier estimates] (95% CI) | 8.3 (7.0, 10.9) | 5.6 (5.4, 6.9) | 10.9 (8.0, 13.8) | 5.8 (5.3, 7.0)
Range in months | 1.2+, 41.5+ | 1.3+, 34.2+ | 1.2+, 41.5+ | 1.4+, 31.2+
+ Denotes ongoing response

Figure 24: Kaplan-Meier Curve for Overall Survival in KEYNOTE-859 (CPS≥1)

Figure 25: Kaplan-Meier Curve for Overall Survival in KEYNOTE-859 (CPS≥10)

An exploratory analysis of OS in the 74 patients with MSI-H tumors irrespective of PD-L1 status showed a HR of 0.34 (95% CI: 0.18, 0.66).

14.11 Esophageal Cancer

First-line Treatment of Locally Advanced Unresectable or Metastatic Esophageal/Gastroesophageal Junction Cancer for Tumors Expressing PD-L1 (CPS≥ 1)

KEYNOTE-590

The efficacy of KEYTRUDA was investigated in KEYNOTE-590 (NCT03189719), a multicenter, randomized, placebo-controlled trial that enrolled 749 patients with metastatic or locally advanced esophageal or gastroesophageal junction (tumors with epicenter 1 to 5 centimeters above the GEJ) carcinoma who were not candidates for surgical resection or definitive chemoradiation. PD-L1 status was centrally determined in tumor specimens in all patients using the PD-L1 IHC 22C3 pharmDx assay. Patients with active autoimmune disease, a medical condition that required immunosuppression, or who received prior systemic therapy in the locally advanced or metastatic setting were ineligible. Randomization was stratified by tumor histology (squamous cell carcinoma vs. adenocarcinoma), geographic region (Asia vs. ex-Asia), and ECOG performance status (0 vs. 1).

Patients were randomized (1:1) to one of the following treatment arms; all study medications were administered via intravenous infusion:

- KEYTRUDA 200 mg on Day 1 of each three-week cycle in combination with cisplatin 80 mg/m^2 IV on Day 1 of each three-week cycle for up to six cycles and FU 800 mg/m^2 IV per day on Day 1 to Day 5 of each three-week cycle, or per local standard for FU administration, for up to 24 months.
- Placebo on Day 1 of each three-week cycle in combination with cisplatin 80 mg/m^2 IV on Day 1 of each three-week cycle for up to six cycles and FU 800 mg/m^2 IV per day on Day 1 to Day 5 of each three-week cycle, or per local standard for FU administration, for up to 24 months.

Treatment with KEYTRUDA or chemotherapy continued until unacceptable toxicity or disease progression. Patients could be treated with KEYTRUDA for up to 24 months in the absence of disease progression. The major efficacy outcome measures were OS and PFS as assessed by the investigator according to RECIST v1.1 (modified to follow a maximum of 10 target lesions and a maximum of 5 target lesions per organ). The study pre-specified analyses of OS and PFS based on squamous cell histology, CPS ≥10, and in all patients. Additional efficacy outcome measures were ORR and DoR, according to modified RECIST v1.1, as assessed by the investigator. Additional analyses of efficacy outcome measures were also conducted based on PD-L1 CPS ≥1.

Among 749 patients, 647 (86%) had tumors expressing PD-L1 CPS ≥ 1. The study population characteristics in patients with PD-L1 CPS ≥ 1 expressing tumors were: median age of 63 years (range: 27 to 89), 41% age 65 or older; 83% male; 36% White, 54% Asian, and 1% Black; 40% had an ECOG PS of 0 and 59% had an ECOG PS of 1. Ninety-one percent had M1 disease and 9% had M0 disease. Seventy-four percent had a tumor histology of squamous cell carcinoma, and 26% had adenocarcinoma.

The trial demonstrated a statistically significant improvement in OS and PFS for patients randomized to KEYTRUDA in combination with chemotherapy compared to chemotherapy; however, an exploratory analysis of OS in the PD-L1 CPS <1 population showed an HR of 0.96 (0.59, 1.55), indicating that the improvement in the ITT population was primarily attributed to the results observed in the subgroup of patients with PD-L1 CPS ≥1.

Table 91 and Figures 26 and 27 summarize the efficacy results for KEYNOTE-590 in patients whose tumors expressed PD-L1 CPS ≥1 and CPS ≥10.

Table 91: Efficacy Results in Patients with Locally Advanced Unresectable or Metastatic Esophageal Cancer in KEYNOTE-590
Endpoint | KEYTRUDA 200 mg every 3 weeks Cisplatin FU n=320 | Placebo Cisplatin FU n=327 | KEYTRUDA 200 mg every 3 weeks Cisplatin FU n=186 | Placebo Cisplatin FU n=197
 | CPS ≥ 1 |  | CPS ≥ 10
OS
Number (%) of events | 222 (69) | 271 (83) | 124 (67) | 165 (84)
Median in months (95% CI) | 12.7 (10.5, 14.4) | 9.8 (8.8, 10.8) | 13.5 (11.1, 15.6) | 9.4 (8.0, 10.7)
Hazard ratio [Based on the stratified Cox proportional hazard model] (95% CI) | 0.71 (0.59, 0.84) |  | 0.62 (0.49, 0.78)
p-Value [Based on a stratified log-rank test; p-Value for CPS ≥ 1 not included (not pre-specified subgroup)] |  |  | <0.0001
PFS
Number of events (%) | 252 (79) | 291 (89) | 140 (75) | 174 (88)
Median in months (95% CI) | 6.3 (6.2, 7.1) | 5.7 (4.6, 6.0) | 7.5 (6.2, 8.2) | 5.5 (4.3, 6.0)
Hazard ratio (95% CI) | 0.62 (0.52, 0.73) |  | 0.51 (0.41, 0.65)
p-Value |  |  | <0.0001
Objective Response Rate
ORR, % [Confirmed complete response or partial response] (95% CI) | 45 (40, 51) | 29 (24, 34) | 51 (44, 59) | 27 (21, 34)
Number (%) of complete responses | 19 (6) | 9 (2.8) | 11 (6) | 5 (2.5)
Number (%) of partial responses | 126 (39) | 85 (26) | 84 (45) | 48 (24)
Duration of Response
Median in months (range) | 8.6 (1.2+, 31.0+) | 5.8 (1.5+, 25.0+) | 10.4 (1.9+, 28.9+) | 5.6 (1.5+, 25.0+)

Figure 26: Kaplan-Meier Curve for Overall Survival in KEYNOTE-590 (CPS ≥1)

Figure 27: Kaplan-Meier Curve for Overall Survival in KEYNOTE-590 (CPS ≥10)

In a pre-specified formal test of OS in patients with PD-L1 CPS ≥ 10 (n=383), the median was 13.5 months (95% CI: 11.1, 15.6) for the KEYTRUDA arm and 9.4 months (95% CI: 8.0, 10.7) for the placebo arm, with a HR of 0.62 (95% CI: 0.49, 0.78; p-Value < 0.0001). In an exploratory analysis, in patients with PD-L1 CPS < 10 (n=347), the median OS was 10.5 months (95% CI: 9.7, 13.5) for the KEYTRUDA arm and 10.6 months (95% CI: 8.8, 12.0) for the placebo arm, with a HR of 0.86 (95% CI: 0.68, 1.10).

Previously Treated Recurrent Locally Advanced or Metastatic Esophageal Cancer for Tumors Expressing PD-L1 (CPS≥ 10)

KEYNOTE-181

The efficacy of KEYTRUDA was investigated in KEYNOTE-181 (NCT02564263), a multicenter, randomized, open-label, active-controlled trial that enrolled 628 patients with recurrent locally advanced or metastatic esophageal cancer who progressed on or after one prior line of systemic treatment for advanced disease. Patients with HER2/neu positive esophageal cancer were required to have received treatment with approved HER2/neu targeted therapy. All patients were required to have tumor specimens for PD-L1 testing at a central laboratory; PD-L1 status was determined using the PD-L1 IHC 22C3 pharmDx assay. Patients with a history of non-infectious pneumonitis that required steroids or current pneumonitis, active autoimmune disease, or a medical condition that required immunosuppression were ineligible.

Patients were randomized (1:1) to receive either KEYTRUDA 200 mg every 3 weeks or investigator's choice of any of the following chemotherapy regimens, all given intravenously: paclitaxel 80-100 mg/m^2 on Days 1, 8, and 15 of every 4-week cycle, docetaxel 75 mg/m^2 every 3 weeks, or irinotecan 180 mg/m^2 every 2 weeks. Randomization was stratified by tumor histology (esophageal squamous cell carcinoma [ESCC] vs. esophageal adenocarcinoma [EAC]/Siewert type I EAC of the gastroesophageal junction [GEJ]), and geographic region (Asia vs. ex-Asia). Treatment with KEYTRUDA or chemotherapy continued until unacceptable toxicity or disease progression. Patients randomized to KEYTRUDA were permitted to continue beyond the first RECIST v1.1 (modified to follow a maximum of 10 target lesions and a maximum of 5 target lesions per organ)-defined disease progression if clinically stable until the first radiographic evidence of disease progression was confirmed at least 4 weeks later with repeat imaging. Patients treated with KEYTRUDA without disease progression could be treated for up to 24 months. Assessment of tumor status was performed every 9 weeks. The major efficacy outcome measure was OS evaluated in the following co-primary populations: patients with ESCC, patients with tumors expressing PD-L1 CPS ≥10, and all randomized patients. Additional efficacy outcome measures were PFS, ORR, and DoR, according to RECIST v1.1, modified to follow a maximum of 10 target lesions and a maximum of 5 target lesions per organ, as assessed by BICR.

A total of 628 patients were enrolled and randomized to KEYTRUDA (n=314) or investigator's treatment of choice (n=314). Of these 628 patients, 167 (27%) had ESCC that expressed PD-L1 with a CPS ≥10. Of these 167 patients, 85 patients were randomized to KEYTRUDA and 82 patients to investigator's treatment of choice [paclitaxel (n=50), docetaxel (n=19), or irinotecan (n=13)]. The baseline characteristics of these 167 patients were: median age of 65 years (range: 33 to 80), 51% age 65 or older; 84% male; 32% White and 68% Asian; 38% had an ECOG PS of 0 and 62% had an ECOG PS of 1. Ninety percent had M1 disease and 10% had M0 disease. Prior to enrollment, 99% of patients had received platinum-based treatment and 84% had also received treatment with a fluoropyrimidine. Thirty-three percent of patients received prior treatment with a taxane.

The observed OS hazard ratio was 0.77 (95% CI: 0.63, 0.96) in patients with ESCC, 0.70 (95% CI: 0.52, 0.94) in patients with tumors expressing PD-L1 CPS ≥10, and 0.89 (95% CI: 0.75, 1.05) in all randomized patients. On further examination in patients whose ESCC tumors expressed PD-L1 (CPS ≥10), an improvement in OS was observed among patients randomized to KEYTRUDA as compared with chemotherapy. Table 92 and Figure 28 summarize the key efficacy measures for KEYNOTE-181 for patients with ESCC CPS ≥10.

Table 92: Efficacy Results in Patients with Recurrent or Metastatic ESCC (CPS ≥10) in KEYNOTE-181
Endpoint | KEYTRUDA 200 mg every 3 weeks n=85 | Chemotherapy n=82
OS
Number (%) of patients with event | 68 (80%) | 72 (88%)
Median in months (95% CI) | 10.3 (7.0, 13.5) | 6.7 (4.8, 8.6)
Hazard ratio [Based on the Cox regression model stratified by geographic region (Asia vs. ex-Asia)] (95% CI) | 0.64 (0.46, 0.90)
PFS
Number (%) of patients with event | 76 (89%) | 76 (93%)
Median in months (95% CI) | 3.2 (2.1, 4.4) | 2.3 (2.1, 3.4)
Hazard ratio (95% CI) | 0.66 (0.48, 0.92)
Objective Response Rate
ORR (95% CI) | 22 (14, 33) | 7 (3, 15)
Number (%) of complete responses | 4 (5) | 1 (1)
Number (%) of partial responses | 15 (18) | 5 (6)
Median duration of response in months (range) | 9.3 (2.1+, 18.8+) | 7.7 (4.3, 16.8+)

Figure 28: Kaplan-Meier Curve for Overall Survival in KEYNOTE-181 (ESCC CPS ≥10)

KEYNOTE-180

The efficacy of KEYTRUDA was investigated in KEYNOTE-180 (NCT02559687), a multicenter, non-randomized, open-label trial that enrolled 121 patients with locally advanced or metastatic esophageal cancer who progressed on or after at least 2 prior systemic treatments for advanced disease. With the exception of the number of prior lines of treatment, the eligibility criteria were similar to and the dosage regimen identical to KEYNOTE-181.

The major efficacy outcome measures were ORR and DoR according to RECIST v1.1, modified to follow a maximum of 10 target lesions and a maximum of 5 target lesions per organ, as assessed by BICR.

Among the 121 patients enrolled, 29% (n=35) had ESCC that expressed PD-L1 CPS ≥10. The baseline characteristics of these 35 patients were: median age of 65 years (range: 47 to 81), 51% age 65 or older; 71% male; 26% White and 69% Asian; 40% had an ECOG PS of 0 and 60% had an ECOG PS of 1. One hundred percent had M1 disease.

The ORR in the 35 patients with ESCC expressing PD-L1 was 20% (95% CI: 8, 37). Among the 7 responding patients, the DoR ranged from 4.2 to 25.1+ months, with 5 patients (71%) having responses of 6 months or longer and 3 patients (57%) having responses of 12 months or longer.

14.12 Cervical Cancer

FIGO 2014 Stage III-IVA Cervical Cancer

The efficacy of KEYTRUDA in combination with CRT (cisplatin and external beam radiation therapy [EBRT] followed by brachytherapy [BT]) was investigated in KEYNOTE-A18 (NCT04221945), a multicenter, randomized, double-blind, placebo-controlled trial that enrolled 1060 patients with cervical cancer who had not previously received any definitive surgery, radiation, or systemic therapy for cervical cancer. There were 599 patients with FIGO 2014 Stage III-IVA disease (tumor involves the lower third of the vagina or the pelvic sidewall, or there is hydronephrosis/non-functioning kidney or spread to adjacent pelvic organs, all without spread to distant organs), and 459 patients with FIGO 2014 Stage IB2-IIB disease (clinical lesion >4 cm confined to the cervix, or clinical lesion of any size with extension beyond the uterus, but which has not extended to the pelvic wall or lower third of the vagina) with positive nodes. Two patients had FIGO 2014 Stage IVB disease. Randomization was stratified by planned type of EBRT (Intensity-modulated radiation therapy [IMRT] or volumetric modulated arc therapy [VMAT] vs. non-IMRT and non-VMAT), stage at screening of cervical cancer (FIGO 2014 Stage IB2-IIB vs. FIGO 2014 Stage III-IVA), and planned total radiotherapy dose (EBRT + brachytherapy dose of <70 Gy vs. ≥70 Gy as per equivalent dose [EQD2]).

Patients were randomized (1:1) to one of two treatment arms:

- KEYTRUDA 200 mg IV every 3 weeks (5 cycles) concurrent with cisplatin 40 mg/m^2 IV weekly (5 cycles, an optional sixth infusion could be administered per local practice), and radiotherapy (EBRT followed by BT), followed by KEYTRUDA 400 mg IV every 6 weeks (15 cycles)
- Placebo IV every 3 weeks (5 cycles) concurrent with cisplatin 40 mg/m^2 IV weekly (5 cycles, an optional sixth infusion could be administered per local practice), and radiotherapy (EBRT followed by BT), followed by placebo IV every 6 weeks (15 cycles)

Treatment continued until RECIST v1.1-defined progression of disease as determined by investigator or unacceptable toxicity.

Assessment of tumor status was performed every 12 weeks from completion of CRT for the first two years, followed by every 24 weeks in year 3, and then annually. The major efficacy outcome measures were PFS as assessed by investigator according to RECIST v1.1, modified to follow a maximum of 10 target lesions and a maximum of 5 target lesions per organ, or histopathologic confirmation, and OS.

Among the 599 patients with FIGO 2014 Stage III-IVA disease, the baseline characteristics were: median age of 52 years (range: 22 to 87), 17% age 65 or older; 36% White, 34% Asian, 2% Black; 38% Hispanic or Latino; 68% ECOG PS 0 and 32% ECOG PS 1; 93% with CPS ≥1; 71% had positive pelvic and/or positive para-aortic lymph node(s) and 29% had neither positive pelvic nor para-aortic lymph node(s); 83% had squamous cell carcinoma and 17% had non-squamous histology. Regarding radiation, 86% of patients received IMRT or VMAT EBRT, and the median EQD2 dose was 87 Gy (range: 7 to 114).

The trial demonstrated statistically significant improvements in PFS and OS in the ITT population. Exploratory analyses of PFS and OS by the stratification factor of FIGO 2014 stage showed that the improvement in the ITT population was primarily attributed to the results seen in the patients with FIGO 2014 Stage III-IVA disease. Table 93 and Figures 29 and 30 summarize the results in exploratory subgroup analyses of 599 patients with FIGO 2014 Stage III-IVA disease.

Table 93: Efficacy Results in KEYNOTE-A18 (Patients with FIGO 2014 Stage III-IVA Cervical Cancer)
Endpoint | KEYTRUDA 200 mg every 3 weeks and 400 mg every 6 weeks with CRT n=295 | Placebo with CRT n=304
OS [Results at the time of pre-specified final analysis for OS]
Number of patients with event (%) | 61 (21) | 90 (30)
Hazard ratio [Based on the unstratified Cox proportional hazard model] (95% CI) | 0.65 (0.47, 0.90)
PFS by Investigator [Results at the time of first pre-specified interim analysis for PFS]
Number of patients with event (%) | 61 (21) | 94 (31)
Median in months (95% CI) | NR (NR, NR) | NR (18.8, NR)
12-month PFS rate (95% CI) | 81% (75, 85) | 70% (64, 76)
Hazard ratio (95% CI) | 0.59 (0.43, 0.81)
CRT = Chemoradiotherapy
NR = not reached

Figure 29: Kaplan-Meier Curve for Overall Survival in KEYNOTE-A18 (Patients with FIGO 2014 Stage III-IVA Cervical Cancer)

Figure 30: Kaplan-Meier Curve for Progression-Free Survival in KEYNOTE-A18 (Patients with FIGO 2014 Stage III-IVA Cervical Cancer)

Persistent, Recurrent, or Metastatic Cervical Cancer for Tumors Expressing PD-L1 (CPS≥ 1)

The efficacy of KEYTRUDA in combination with paclitaxel and cisplatin or paclitaxel and carboplatin, with or without bevacizumab, was investigated in KEYNOTE-826 (NCT03635567), a multicenter, randomized, double-blind, placebo-controlled trial that enrolled 617 patients with persistent, recurrent, or first-line metastatic cervical cancer who had not been treated with chemotherapy except when used concurrently as a radio-sensitizing agent. Patients were enrolled regardless of tumor PD-L1 expression status. Patients with autoimmune disease that required systemic therapy within 2 years of treatment or a medical condition that required immunosuppression were ineligible. Randomization was stratified by metastatic status at initial diagnosis, investigator decision to use bevacizumab, and PD-L1 status (CPS <1 vs. CPS 1 to <10 vs. CPS ≥10). Patients were randomized (1:1) to one of the two treatment groups:

- Treatment Group 1: KEYTRUDA 200 mg plus chemotherapy with or without bevacizumab
- Treatment Group 2: Placebo plus chemotherapy with or without bevacizumab

The investigator selected one of the following four treatment regimens prior to randomization:

1. Paclitaxel 175 mg/m^2 + cisplatin 50 mg/m^2
2. Paclitaxel 175 mg/m^2 + cisplatin 50 mg/m^2 + bevacizumab 15 mg/kg
3. Paclitaxel 175 mg/m^2 + carboplatin AUC 5 mg/mL/min
4. Paclitaxel 175 mg/m^2 + carboplatin AUC 5 mg/mL/min + bevacizumab 15 mg/kg

All study medications were administered as an intravenous infusion. All study treatments were administered on Day 1 of each 3-week treatment cycle. Cisplatin could be administered on Day 2 of each 3-week treatment cycle. Treatment with KEYTRUDA continued until RECIST v1.1-defined progression of disease, unacceptable toxicity, or a maximum of 24 months. Administration of KEYTRUDA was permitted beyond RECIST-defined disease progression if the patient was clinically stable and considered to be deriving clinical benefit by the investigator. Assessment of tumor status was performed every 9 weeks for the first year, followed by every 12 weeks thereafter. The main efficacy outcome measures were OS and PFS as assessed by investigator according to RECIST v1.1, modified to follow a maximum of 10 target lesions and a maximum of 5 target lesions per organ. Additional efficacy outcome measures were ORR and DoR, according to RECIST v1.1, as assessed by investigator.

Of the 617 enrolled patients, 548 patients (89%) had tumors expressing PD-L1 with a CPS ≥1. Among these 548 enrolled patients with tumors expressing PD-L1, 273 patients were randomized to KEYTRUDA in combination with chemotherapy with or without bevacizumab, and 275 patients were randomized to placebo in combination with chemotherapy with or without bevacizumab. Sixty-three percent of the 548 patients received bevacizumab as part of study treatment. The baseline characteristics of the 548 patients were: median age of 51 years (range: 22 to 82), 16% age 65 or older; 59% White, 18% Asian, 6% American Indian or Alaska Native, and 1% Black; 37% Hispanic or Latino; 56% ECOG performance status 0 and 43% ECOG performance status 1. Seventy-five percent had squamous cell carcinoma, 21% adenocarcinoma, and 5% adenosquamous histology, and 32% of patients had metastatic disease at diagnosis. At study entry, 21% of patients had metastatic disease only and 79% had persistent or recurrent disease with or without distant metastases, of whom 39% had received prior chemoradiation only and 17% had received prior chemoradiation plus surgery.

A statistically significant improvement in OS and PFS was demonstrated in patients randomized to receive KEYTRUDA compared with patients randomized to receive placebo. An updated OS analysis was conducted at the time of final analysis when 354 deaths in the CPS ≥1 population were observed. Table 94 and Figure 31 summarize the key efficacy measures for KEYNOTE-826 for patients with tumors expressing PD-L1 (CPS ≥1).

Table 94: Efficacy Results in Patients with Persistent, Recurrent, or Metastatic Cervical Cancer (CPS ≥1) in KEYNOTE-826
Endpoint | KEYTRUDA 200 mg every 3 weeks and chemotherapy [Chemotherapy (paclitaxel and cisplatin or paclitaxel and carboplatin)] with or without bevacizumab n=273 | Placebo and chemotherapy with or without bevacizumab n=275
OS
Number of patients with event (%) | 118 (43.2) | 154 (56.0)
Median in months (95% CI) | NR (19.8, NR) | 16.3 (14.5, 19.4)
Hazard ratio [Based on the stratified Cox proportional hazard model] (95% CI) | 0.64 (0.50, 0.81)
p-Value [p-Value (one-sided) is compared with the allocated alpha of 0.0055 for this interim analysis (with 72% of the planned number of events for final analysis)] | 0.0001
Updated OS
Number of patients with event (%) | 153 (56.0%) | 201 (73.1%)
Median in months (95% CI) | 28.6 (22.1, 38.0) | 16.5 (14.5, 20.0)
Hazard ratio (95% CI) | 0.60 (0.49, 0.74)
PFS
Number of patients with event (%) | 157 (57.5) | 198 (72.0)
Median in months (95% CI) | 10.4 (9.7, 12.3) | 8.2 (6.3, 8.5)
Hazard ratio (95% CI) | 0.62 (0.50, 0.77)
p-Value [p-Value (one-sided) is compared with the allocated alpha of 0.0014 for this interim analysis (with 82% of the planned number of events for final analysis)] | < 0.0001
Objective Response Rate
ORR [Response: Best objective response as confirmed complete response or partial response] (95% CI) | 68% (62, 74) | 50% (44, 56)
Complete response rate | 23% | 13%
Partial response rate | 45% | 37%
Duration of Response
Median in months (range) | 18.0 (1.3+, 24.2+) | 10.4 (1.5+, 22.0+)
+ Denotes ongoing response
NR = not reached

Figure 31: Kaplan-Meier Curve for Overall Survival in KEYNOTE-826 (CPS ≥1) [Treatment arms include KEYTRUDA plus chemotherapy, with or without bevacizumab, versus placebo plus chemotherapy, with or without bevacizumab.] , [Based on the protocol-specified final OS analysis]

Previously Treated Recurrent or Metastatic Cervical Cancer for Tumors Expressing PD-L1 (CPS≥ 1)

The efficacy of KEYTRUDA was investigated in 98 patients with recurrent or metastatic cervical cancer enrolled in a single cohort (Cohort E) in KEYNOTE-158 (NCT02628067), a multicenter, non-randomized, open-label, multi-cohort trial. The trial excluded patients with autoimmune disease or a medical condition that required immunosuppression. Patients received KEYTRUDA 200 mg intravenously every 3 weeks until unacceptable toxicity or documented disease progression. Patients with initial radiographic disease progression could receive additional doses of treatment during confirmation of progression unless disease progression was symptomatic, was rapidly progressive, required urgent intervention, or occurred with a decline in performance status. Patients without disease progression could be treated for up to 24 months. Assessment of tumor status was performed every 9 weeks for the first 12 months, and every 12 weeks thereafter. The major efficacy outcome measures were ORR according to RECIST v1.1, modified to follow a maximum of 10 target lesions and a maximum of 5 target lesions per organ, as assessed by BICR, and DoR.

Among the 98 patients in Cohort E, 77 (79%) had tumors that expressed PD-L1 with a CPS ≥ 1 and received at least one line of chemotherapy in the metastatic setting. PD-L1 status was determined using the IHC 22C3 pharmDx assay. The baseline characteristics of these 77 patients were: median age of 45 years (range: 27 to 75); 81% White, 14% Asian, and 3% Black; 32% ECOG PS of 0 and 68% ECOG PS of 1; 92% had squamous cell carcinoma, 6% adenocarcinoma, and 1% adenosquamous histology; 95% had M1 disease and 5% had recurrent disease; and 35% had one and 65% had two or more prior lines of therapy in the recurrent or metastatic setting.

No responses were observed in patients whose tumors did not have PD-L1 expression (CPS <1). Efficacy results are summarized in Table 95 for patients with PD-L1 expression (CPS ≥1).

Table 95: Efficacy Results in Patients with Recurrent or Metastatic Cervical Cancer (CPS ≥1) in KEYNOTE-158
Endpoint | KEYTRUDA 200 mg every 3 weeks n=77 [Median follow-up time of 11.7 months (range 0.6 to 22.7 months)]
Objective Response Rate
ORR (95% CI) | 14.3% (7.4, 24.1)
Complete response rate | 2.6%
Partial response rate | 11.7%
Duration of Response
Median in months (range) | NR (4.1, 18.6+) [Based on patients (n=11) with a response by independent review]
% with duration ≥6 months | 91%
+ Denotes ongoing response
NR = not reached

14.13 Hepatocellular Carcinoma

Previously Treated HCC

The efficacy of KEYTRUDA was investigated in KEYNOTE-394 (NCT03062358), a multicenter, randomized, placebo-controlled, double-blind trial conducted in Asia in patients with Barcelona Clinic Liver Cancer (BCLC) Stage B or C HCC, who were previously treated with sorafenib or oxaliplatin-based chemotherapy and who were not amenable to or were refractory to local-regional therapy. Patients were also required to have Child-Pugh A liver function.

Patients with hepatitis B had treated controlled disease (HBV viral load <2000 IU/mL or <10^4 copies/mL). Patients with an autoimmune disease that required systemic therapy within 2 years of treatment or a medical condition that required immunosuppression were ineligible. Patients with hepatic encephalopathy, main branch portal venous invasion, clinically apparent ascites, or esophageal or gastric variceal bleeding within the last 6 months were also ineligible.

Randomization was stratified by prior treatment: sorafenib vs. oxaliplatin-based chemotherapy, macrovascular invasion, and etiology (active HBV vs. others (active HCV, non-infected)). Patients were randomized (2:1) to receive pembrolizumab 200 mg intravenously every 3 weeks or placebo.

Treatment with KEYTRUDA continued until RECIST v1.1-defined progression of disease as determined by BICR, unacceptable toxicity, or a maximum of 24 months. Assessment of tumor status was performed every 6 weeks. The main efficacy outcome measure was OS. Additional efficacy outcome measures were PFS, ORR, and DoR, as assessed by BICR using RECIST v1.1, modified to follow a maximum of 10 target lesions and a maximum of 5 target lesions per organ.

The study enrolled 453 patients, and 360 (79%) had active hepatitis B. The population characteristics in patients with active hepatitis B were: median age of 52 years (range: 23 to 82), 16% age 65 or older; 86% male; 100% Asian; 42% ECOG PS of 0 and 58% ECOG PS of 1; 90% received prior sorafenib and 10% received prior oxaliplatin-based chemotherapy. Patient characteristics also included extrahepatic disease (77%), macrovascular invasion (10%), BCLC stage C (93%) and B (7%), and baseline AFP ≥200 ng/mL (57%).

KEYNOTE-394 demonstrated improved OS in patients with HCC secondary to hepatitis B randomized to KEYTRUDA compared with placebo. Efficacy results are summarized in Table 96 and Figure 32.

Table 96: Efficacy Results in Patients with Hepatocellular Carcinoma in KEYNOTE-394
Endpoint | KEYTRUDA 200 mg every 3 weeks n=236 | Placebo n=124
OS [Results at the pre-specified final OS analysis]
Number (%) of patients with events | 172 (73) | 105 (85)
Median in months (95% CI) | 13.9 (12.5, 17.9) | 13.0 (10.1, 15.6)
Hazard ratio [Based on the stratified Cox proportional hazard model] (95% CI) | 0.78 (0.61, 0.99)
PFS [Results at pre-specified interim OS analysis]
Number (%) of patients with events | 189 (80) | 108 (87)
Median in months (95% CI) | 2 (1.4, 2.7) | 2.3 (1.4, 2.8)
Hazard ratio (95% CI) | 0.78 (0.61, 1.00)
Objective Response Rate
ORR [Confirmed complete response or partial response] (95% CI) | 11% (7, 16) | 1.6% (0.2, 5.7)
Number (%) of complete responses | 2 (0.9%) | 1 (0.8%)
Number (%) of partial responses | 24 (10%) | 1 (0.8%)
Duration of Response | n=28 | n=2
Median in months [Based on Kaplan-Meier estimate] (range) | 23.9 (2.6+, 44.4+) | 5.6 (3.0+, 5.6)
+ Denotes ongoing response

Figure 32: Kaplan-Meier Curve for Overall Survival in KEYNOTE-394

14.14 Biliary Tract Cancer

The efficacy of KEYTRUDA in combination with gemcitabine and cisplatin chemotherapy was investigated in KEYNOTE-966 (NCT04003636), a multicenter, randomized, double-blind, placebo-controlled trial that enrolled 1069 patients with locally advanced unresectable or metastatic BTC, who had not received prior systemic therapy in the advanced disease setting. Patients with autoimmune disease that required systemic therapy within 2 years of treatment or a medical condition that required immunosuppression were ineligible. Randomization was stratified by region (Asia vs. non-Asia), locally advanced versus metastatic, and site of origin (gallbladder, intrahepatic or extrahepatic cholangiocarcinoma).

Patients were randomized (1:1) to KEYTRUDA 200 mg on Day 1 plus gemcitabine 1000 mg/m^2 and cisplatin 25 mg/m^2 on Day 1 and Day 8 every 3 weeks, or placebo on Day 1 plus gemcitabine 1000 mg/m^2 and cisplatin 25 mg/m^2 on Day 1 and Day 8 every 3 weeks. Study medications were administered via intravenous infusion. Treatment continued until unacceptable toxicity or disease progression. For pembrolizumab, treatment continued for a maximum of 35 cycles, or approximately 24 months. For gemcitabine, treatment could be continued beyond 8 cycles while for cisplatin, treatment could be administered for a maximum of 8 cycles.

Administration of KEYTRUDA with chemotherapy was permitted beyond RECIST-defined disease progression if the patient was clinically stable and considered by the investigator to be deriving clinical benefit. Assessment of tumor status was performed at baseline and then every 6 weeks through 54 weeks, followed by every 12 weeks thereafter.

Study population characteristics were median age of 64 years (range: 23 to 85), 47% age 65 or older; 52% male; 49% White, 46% Asian, 1.3% Black or African American; 10% Hispanic or Latino; 46% ECOG PS of 0 and 54% ECOG PS of 1; 31% of patients had a history of hepatitis B infection, and 3% had a history of hepatitis C infection.

The major efficacy outcome measure was OS. Additional efficacy outcome measures were PFS, ORR and DoR as assessed by BICR according to RECIST v1.1, modified to follow a maximum of 10 target lesions and a maximum of 5 target lesions per organ.

Table 97 and Figure 33 summarize the efficacy results for KEYNOTE-966.

Table 97: Efficacy Results in KEYNOTE-966
Endpoint | KEYTRUDA 200 mg every 3 weeks with gemcitabine/cisplatin n=533 | Placebo with gemcitabine/cisplatin n=536
OS [Results at the pre-specified final OS analysis]
Number of patients with event (%) | 414 (78%) | 443 (83%)
Median in months (95% CI) | 12.7 (11.5, 13.6) | 10.9 (9.9, 11.6)
Hazard ratio [Based on the stratified Cox proportional hazard model] (95% CI) | 0.83 (0.72, 0.95)
p-Value [One-sided p-Value based on a stratified log-rank test] | 0.0034
PFS [Results at pre-specified final analysis of PFS and ORR]
Number (%) of patients with event | 361 (68%) | 391 (73%)
Median in months (95% CI) | 6.5 (5.7, 6.9) | 5.6 (5.1, 6.6)
Hazard ratio (95% CI) | 0.86 (0.75, 1.00)
p-Value | NS
Objective Response Rate
ORR [Confirmed complete response or partial response] (95% CI) | 29% (25, 33) | 29% (25, 33)
Number (%) of complete responses | 11 (2.1%) | 7 (1.3%)
Number (%) of partial responses | 142 (27%) | 146 (27%)
p-Value [One-sided p-Value based on the stratified Miettinen and Nurminen analysis] | NS
Duration of Response | n=156 | n=152
Median in months [Based on Kaplan-Meier estimate] (95% CI) | 8.3 (6.9, 10.2) | 6.8 (5.7, 7.1)
NS = not significant

Figure 33: Kaplan-Meier Curve for Overall Survival in KEYNOTE-966

14.15 Merkel Cell Carcinoma

The efficacy of KEYTRUDA was investigated in KEYNOTE-017 (NCT02267603) and KEYNOTE-913 (NCT03783078), two multicenter, non-randomized, open-label trials that enrolled 105 patients with recurrent locally advanced or metastatic MCC who had not received prior systemic therapy for their advanced disease. Patients with active autoimmune disease or a medical condition that required immunosuppression were ineligible.

Patients received KEYTRUDA 2 mg/kg (KEYNOTE-017) or 200 mg (KEYNOTE-913) every 3 weeks until unacceptable toxicity or disease progression that was symptomatic, rapidly progressive, required urgent intervention, occurred with a decline in performance status, or was confirmed at least 4 weeks later with repeat imaging. Patients without disease progression were treated for up to 24 months.

The major efficacy outcome measures were ORR and DoR as assessed by BICR per RECIST v1.1.

Among the 105 patients enrolled, the median age was 73 years (range: 38 to 91), 79% were age 65 or older; 62% were male; 80% were White, race in 19% was unknown or missing, and 1% were Asian; 53% had ECOG PS of 0, and 47% had ECOG PS of 1. Thirteen percent had stage IIIB disease and 84% had stage IV. Seventy-six percent of patients had prior surgery and 51% had prior radiation therapy.

Efficacy results are summarized in Table 98.

Table 98: Efficacy Results in KEYNOTE-017 and KEYNOTE-913
Endpoint | KEYNOTE-017 KEYTRUDA 2 mg/kg every 3 weeks n=50 | KEYNOTE-913 KEYTRUDA 200 mg or 2 mg/kg every 3 weeks n=55
Objective Response Rate
ORR (95% CI) | 56% (41, 70) | 49% (35, 63)
Complete responses, n (%) | 12 (24%) | 9 (16%)
Partial responses, n (%) | 16 (32%) | 18 (33%)
Duration of Response | n=28 | n=27
Median DoR in months (range) | NR (5.9, 34.5+) | NR (4.8, 25.4+)
Patients with duration ≥6 months, n (%) | 27 (96%) | 25 (93%)
Patients with duration ≥12 months, n (%) | 15 (54%) | 19 (70%)
+ Denotes ongoing response
NR = not reached

14.16 Renal Cell Carcinoma

First-line treatment with axitinib

KEYNOTE-426

The efficacy of KEYTRUDA in combination with axitinib was investigated in KEYNOTE-426 (NCT02853331), a randomized, multicenter, open-label trial conducted in 861 patients who had not received systemic therapy for advanced RCC. Patients were enrolled regardless of PD-L1 tumor expression status. Patients with active autoimmune disease requiring systemic immunosuppression within the last 2 years were ineligible. Randomization was stratified by International Metastatic RCC Database Consortium (IMDC) risk categories (favorable versus intermediate versus poor) and geographic region (North America versus Western Europe versus "Rest of the World").

Patients were randomized (1:1) to one of the following treatment arms:

- KEYTRUDA 200 mg intravenously every 3 weeks up to 24 months in combination with axitinib 5 mg orally, twice daily. Patients who tolerated axitinib 5 mg twice daily for 2 consecutive cycles (6 weeks) could increase to 7 mg and then subsequently to 10 mg twice daily. Axitinib could be interrupted or reduced to 3 mg twice daily and subsequently to 2 mg twice daily to manage toxicity.
- Sunitinib 50 mg orally, once daily for 4 weeks and then off treatment for 2 weeks.

Treatment with KEYTRUDA and axitinib continued until RECIST v1.1-defined progression of disease or unacceptable toxicity. Administration of KEYTRUDA and axitinib was permitted beyond RECIST-defined disease progression if the patient was clinically stable and considered to be deriving clinical benefit by the investigator. Assessment of tumor status was performed at baseline, after randomization at Week 12, then every 6 weeks thereafter until Week 54, and then every 12 weeks thereafter.

The study population characteristics were: median age of 62 years (range: 26 to 90), 38% age 65 or older; 73% male; 79% White and 16% Asian; 20% and 80% of patients had a baseline KPS of 70 to 80 and 90 to 100, respectively; and patient distribution by IMDC risk categories was 31% favorable, 56% intermediate, and 13% poor.

The main efficacy outcome measures were OS and PFS as assessed by BICR according to RECIST v1.1, modified to follow a maximum of 10 target lesions and a maximum of 5 target lesions per organ. Additional efficacy outcome measures included ORR, as assessed by BICR. A statistically significant improvement in OS was demonstrated at the first pre-specified interim analysis in patients randomized to KEYTRUDA in combination with axitinib compared with sunitinib. The trial also demonstrated statistically significant improvements in PFS and ORR. An updated OS analysis was conducted when 418 deaths were observed based on the planned number of deaths for the pre-specified final analysis. Table 99 and Figure 34 summarize the efficacy results for KEYNOTE-426.

Table 99: Efficacy Results in KEYNOTE-426
Endpoint | KEYTRUDA 200 mg every 3 weeks and Axitinib | Sunitinib
Endpoint | n=432 | n=429
OS
Number of patients with event (%) | 59 (14%) | 97 (23%)
Median in months (95% CI) | NR (NR, NR) | NR (NR, NR)
Hazard ratio [Based on the stratified Cox proportional hazard model] (95% CI) | 0.53 (0.38, 0.74)
p-Value [Based on stratified log-rank test] | <0.0001 [p-Value (one-sided) is compared with the allocated alpha of 0.0001 for this interim analysis (with 39% of the planned number of events for final analysis).]
Updated OS
Number of patients with event (%) | 193 (45%) | 225 (52%)
Median in months (95% CI) | 45.7 (43.6, NR) | 40.1 (34.3, 44.2)
Hazard ratio (95% CI) | 0.73 (0.60, 0.88)
PFS
Number of patients with event (%) | 183 (42%) | 213 (50%)
Median in months (95% CI) | 15.1 (12.6, 17.7) | 11.0 (8.7, 12.5)
Hazard ratio (95% CI) | 0.69 (0.56, 0.84)
p-Value | 0.0001 [p-Value (one-sided) is compared with the allocated alpha of 0.0013 for this interim analysis (with 81% of the planned number of events for final analysis).]
Objective Response Rate
ORR [Response: Best objective response as confirmed complete response or partial response] (95% CI) | 59% (54, 64) | 36% (31, 40)
Complete response rate | 6% | 2%
Partial response rate | 53% | 34%
p-Value [Based on Miettinen and Nurminen method stratified by IMDC risk group and geographic region] | <0.0001
NR = not reached

Figure 34: Kaplan-Meier Curve for Updated Overall Survival in KEYNOTE-426

In an exploratory analysis, the updated analysis of OS in patients with IMDC favorable, intermediate, intermediate/poor, and poor risk demonstrated a HR of 1.17 (95% CI: 0.76, 1.80), 0.67 (95% CI: 0.52, 0.86), 0.64 (95% CI: 0.52, 0.80), and 0.51 (95% CI: 0.32, 0.81), respectively.

First-line treatment with lenvatinib

KEYNOTE-581

The efficacy of KEYTRUDA in combination with lenvatinib was investigated in KEYNOTE-581 (NCT02811861), a multicenter, open-label, randomized trial conducted in 1069 patients with advanced RCC in the first-line setting. Patients were enrolled regardless of PD-L1 tumor expression status. Patients with active autoimmune disease or a medical condition that required immunosuppression were ineligible. Randomization was stratified by geographic region (North America versus Western Europe versus "Rest of the World") and Memorial Sloan Kettering Cancer Center (MSKCC) prognostic groups (favorable versus intermediate versus poor risk).

Patients were randomized (1:1:1) to one of the following treatment arms:

- KEYTRUDA 200 mg intravenously every 3 weeks up to 24 months in combination with lenvatinib 20 mg orally once daily.
- Lenvatinib 18 mg orally once daily in combination with everolimus 5 mg orally once daily.
- Sunitinib 50 mg orally once daily for 4 weeks then off treatment for 2 weeks.

Treatment continued until unacceptable toxicity or disease progression. Administration of KEYTRUDA with lenvatinib was permitted beyond RECIST-defined disease progression if the patient was clinically stable and considered by the investigator to be deriving clinical benefit. KEYTRUDA was continued for a maximum of 24 months; however, treatment with lenvatinib could be continued beyond 24 months. Assessment of tumor status was performed at baseline and then every 8 weeks.

The study population characteristics were: median age of 62 years (range: 29 to 88 years), 42% age 65 or older; 75% male; 74% White, 21% Asian, 1% Black, and 2% other races; 18% and 82% of patients had a baseline KPS of 70 to 80 and 90 to 100, respectively; patient distribution by MSKCC risk categories was 27% favorable, 64% intermediate, and 9% poor. Common sites of metastases in patients were lung (68%), lymph node (45%), and bone (25%).

The major efficacy outcome measures were PFS, as assessed by independent radiologic review (IRC) according to RECIST v1.1, and OS. Additional efficacy outcome measures included confirmed ORR as assessed by IRC. KEYTRUDA in combination with lenvatinib demonstrated statistically significant improvements in PFS, OS, and ORR compared with sunitinib. An updated OS analysis was conducted when 304 deaths were observed based on the planned number of deaths for the pre-specified final analysis. Table 100 and Figures 35 and 36 summarize the efficacy results for KEYNOTE-581.

Table 100: Efficacy Results in KEYNOTE-581
Endpoint | KEYTRUDA 200 mg every 3 weeks and Lenvatinib | Sunitinib
Endpoint | n=355 | n=357
Progression-Free Survival (PFS)
Number of events, n (%) | 160 (45%) | 205 (57%)
Progressive disease | 145 (41%) | 196 (55%)
Death | 15 (4%) | 9 (3%)
Median PFS in months (95% CI) | 23.9 (20.8, 27.7) | 9.2 (6.0, 11.0)
Hazard ratio [Hazard ratio is based on a Cox Proportional Hazards Model. Stratified by geographic region and MSKCC prognostic groups.] (95% CI) | 0.39 (0.32, 0.49)
p-Value [Two-sided p-Value based on stratified log-rank test.] | <0.0001
Overall Survival (OS)
Number of deaths, n (%) | 80 (23%) | 101 (28%)
Median OS in months (95% CI) | NR (33.6, NR) | NR (NR, NR)
Hazard ratio (95% CI) | 0.66 (0.49, 0.88)
p-Value | 0.0049
Updated OS
Number of deaths, n (%) | 149 (42%) | 159 (45%)
Median OS in months (95% CI) | 53.7 (48.7, NR) | 54.3 (40.9, NR)
Hazard ratio (95% CI) | 0.79 (0.63, 0.99)
Objective Response Rate (Confirmed)
ORR, n (%) | 252 (71%) | 129 (36%)
(95% CI) | (66, 76) | (31, 41)
Complete response rate | 16% | 4%
Partial response rate | 55% | 32%
p-Value [Two-sided p-Value based upon CMH test.] | <0.0001
Tumor assessments were based on RECIST 1.1; only confirmed responses are included for ORR.
Data cutoff date = 28 Aug 2020, Updated OS cutoff date = 31 July 2022
CI = confidence interval; NR= Not reached

Figure 35: Kaplan-Meier Curve for PFS in KEYNOTE-581

Figure 36: Kaplan-Meier Curve for Updated Overall Survival in KEYNOTE-581

KEYNOTE-B61

The efficacy of KEYTRUDA in combination with lenvatinib was investigated in KEYNOTE-B61 (NCT04704219), a multicenter, single-arm trial that enrolled 160 patients with advanced or metastatic non-clear cell RCC in the first-line setting. Patients with active autoimmune disease or a medical condition that required immunosuppression were ineligible.

Patients received KEYTRUDA 400 mg every 6 weeks in combination with lenvatinib 20 mg orally once daily. KEYTRUDA was continued for a maximum of 24 months; however, lenvatinib could be continued beyond 24 months. Treatment continued until unacceptable toxicity or disease progression. Administration of KEYTRUDA with lenvatinib was permitted beyond RECIST-defined disease progression if the patient was considered by the investigator to be deriving clinical benefit.

Among the 158 treated patients, the baseline characteristics were: median age of 60 years (range: 24 to 87 years); 71% male; 86% White, 8% Asian, and 3% Black; <1% Hispanic or Latino; 22% and 78% of patients had a baseline KPS of 70 to 80 and 90 to 100, respectively; histologic subtypes were 59% papillary, 18% chromophobe, 4% translocation, <1% medullary, 13% unclassified, and 6% other; patient distribution by IMDC risk categories was 35% favorable, 54% intermediate, and 10% poor. Common sites of metastases in patients were lymph node (65%), lung (35%), bone (30%), and liver (21%).

The major efficacy outcome measure was ORR as assessed by BICR using RECIST 1.1. Additional efficacy outcome measures included DOR as assessed by BICR using RECIST 1.1. Efficacy results are summarized in Table 101.

Table 101: Efficacy Results in KEYNOTE-B61
Endpoint | KEYTRUDA 400 mg every 6 weeks and Lenvatinib n=158
Objective Response Rate (Confirmed)
ORR (95% CI) | 51% (43, 59)
Complete response | 8%
Partial response | 42%
Duration of Response [Based on Kaplan-Meier estimates]
Median in months (range) | 19.5 (1.5+, 23.5+)
CI = confidence interval
+ Denotes ongoing response

Adjuvant Treatment of RCC (KEYNOTE‑564)

The efficacy of KEYTRUDA was investigated as adjuvant therapy for RCC in KEYNOTE-564 (NCT03142334), a multicenter, randomized (1:1), double-blind, placebo-controlled trial in 994 patients with intermediate-high or high risk of recurrence of RCC, or M1 no evidence of disease (NED). The intermediate-high risk category included: pT2 with Grade 4 or sarcomatoid features; pT3, any Grade without nodal involvement (N0) or distant metastases (M0). The high risk category included: pT4, any Grade N0 and M0; any pT, any Grade with nodal involvement and M0. The M1 NED category included patients with metastatic disease who had undergone complete resection of primary and metastatic lesions. Patients must have undergone a partial nephroprotective or radical complete nephrectomy (and complete resection of solid, isolated, soft tissue metastatic lesion(s) in M1 NED participants) with negative surgical margins ≥4 weeks prior to the time of screening. Patients were excluded from the trial if they had received prior systemic therapy for advanced RCC. Patients with active autoimmune disease or a medical condition that required immunosuppression were also ineligible. Patients were randomized to KEYTRUDA 200 mg administered intravenously every 3 weeks or placebo for up to 1 year until disease recurrence or unacceptable toxicity. Randomization was stratified by metastasis status (M0, M1 NED); M0 group was further stratified by ECOG PS (0,1) and geographic region (US, non-US).

The study population characteristics were: median age of 60 years (range: 25 to 84), 33% age 65 or older; 71% male; 75% White, 14% Asian, 9% Unknown, 1% Black or African American, 1% American Indian or Alaska Native, 1% Multiracial; 13% Hispanic or Latino, 78% Not Hispanic or Latino, 8% Unknown; and 85% ECOG PS of 0 and 15% ECOG PS of 1. Ninety-four percent of patients enrolled had N0 disease; 11% had sarcomatoid features; 86% were intermediate-high risk; 8% were high risk; and 6% were M1 NED. Ninety-two percent of patients had a radical nephrectomy, and 8% had a partial nephrectomy.

The major efficacy outcome measure was investigator-assessed disease-free survival (DFS), defined as time to recurrence, metastasis, or death. An additional outcome measure was OS. Statistically significant improvements in DFS and OS were demonstrated at pre-specified interim analyses in patients randomized to the KEYTRUDA arm compared with placebo. Efficacy results are summarized in Table 102 and Figures 37 and 38.

Table 102: Efficacy Results in KEYNOTE-564
Endpoint | KEYTRUDA 200 mg every 3 weeks n=496 | Placebo n=498
DFS
Number (%) of patients with event | 109 (22%) | 151 (30%)
Median in months (95% CI) | NR | NR
Hazard ratio [Based on the stratified Cox proportional hazard model] (95% CI) | 0.68 (0.53, 0.87)
p-Value [Based on stratified log-rank test] | 0.0010 [p-Value (one-sided) is compared with a boundary of 0.0114.]
24-month DFS rate (95% CI) | 77% (73, 81) | 68% (64, 72)
OS
Number (%) of patients with event | 55 (11%) | 86 (17%)
Median in months (95% CI) | NR (NR, NR) | NR (NR, NR)
Hazard ratio (95% CI) | 0.62 (0.44, 0.87)
p-Value | 0.0024 [p-Value (one-sided) is compared with a boundary of 0.0072.]
48-month OS rate (95% CI) | 91% (88, 93) | 86% (83, 89)
NR = not reached

Figure 37: Kaplan-Meier Curve for Disease-Free Survival in KEYNOTE-564

Figure 38: Kaplan-Meier Curve for Overall Survival in KEYNOTE-564

14.17 Endometrial Carcinoma

In Combination with Paclitaxel and Carboplatin for the Treatment of Primary Advanced or Recurrent Endometrial Carcinoma

The efficacy of KEYTRUDA in combination with paclitaxel and carboplatin was investigated in KEYNOTE-868/NRG-GY018 (NCT03914612), a multicenter, randomized, double-blind, placebo-controlled trial in 810 patients with advanced or recurrent endometrial carcinoma. The study design included two separate cohorts based on MMR status; 222 (27%) patients were in dMMR cohort, 588 (73%) patients were in pMMR cohort. The trial enrolled measurable Stage III, measurable Stage IVA, Stage IVB or recurrent endometrial cancer (with or without measurable disease). Patients who had not received prior systemic therapy or had received prior chemotherapy in the adjuvant setting were eligible. Patients who had received prior adjuvant chemotherapy were only eligible if their chemotherapy-free interval was at least 12 months. Patients with endometrial sarcoma, including carcinosarcoma, or patients with active autoimmune disease or a medical condition that required immunosuppression were ineligible. Randomization was stratified according to MMR status, ECOG PS (0 or 1 vs. 2), and prior adjuvant chemotherapy.

Patients were randomized (1:1) to one of the following treatment arms:

- KEYTRUDA 200 mg every 3 weeks, paclitaxel 175 mg/m^2 and carboplatin AUC 5 mg/mL/min for 6 cycles, followed by KEYTRUDA 400 mg every 6 weeks for up to 14 cycles.
- Placebo every 3 weeks, paclitaxel 175 mg/m^2 and carboplatin AUC 5 mg/mL/min for 6 cycles, followed by placebo every 6 weeks for up to 14 cycles.

All study medications were administered as an intravenous infusion on Day 1 of each treatment cycle. Treatment continued until disease progression, unacceptable toxicity, or a maximum of 20 cycles (up to approximately 24 months). Patients with measurable disease who had RECIST-defined stable disease or partial response at the completion of cycle 6 were permitted to continue receiving paclitaxel and carboplatin with KEYTRUDA or placebo for up to 10 cycles as determined by the investigator. Assessment of tumor status was performed every 9 weeks for the first 9 months and then every 12 weeks thereafter. The major efficacy outcome measure was PFS as assessed by the investigator according to RECIST 1.1. An additional efficacy outcome measure was OS.

The dMMR population characteristics were: median age of 66 years (range: 37 to 86), 55% age 65 or older; 79% White, 9% Black, and 3% Asian; 5% Hispanic or Latino; 64% ECOG PS of 0, 33% ECOG PS of 1, and 3% ECOG PS of 2; 61% had recurrent disease and 39% had primary or persistent disease; 5% received prior adjuvant chemotherapy and 43% received prior radiotherapy. The histologic subtypes were endometrioid carcinoma (81%), adenocarcinoma NOS (11%), serous carcinoma (2%), and other (6%).

The pMMR population characteristics were: median age of 66 years (range: 29 to 94), 54% age 65 or older; 72% White, 16% Black, and 5% Asian; 6% Hispanic or Latino; 67% ECOG PS of 0, 30% ECOG PS of 1, and 3% ECOG PS of 2; 56% had recurrent disease and 44% had primary or persistent disease; 26% received prior adjuvant chemotherapy and 41% received prior radiotherapy. The histologic subtypes were endometrioid carcinoma (52%), serous carcinoma (26%), adenocarcinoma NOS (10%), clear cell carcinoma (7%), and other (5%).

The trial demonstrated statistically significant improvements in PFS for patients randomized to KEYTRUDA in combination with paclitaxel and carboplatin compared to placebo in combination with paclitaxel and carboplatin in both the dMMR and pMMR populations. Table 103 and Figures 39 and 40 summarize the efficacy results for KEYNOTE-868 by MMR status. At the time of the PFS analysis, OS data were not mature with 12% deaths in the dMMR population and 17% deaths in the pMMR population.

Table 103: Efficacy Results in KEYNOTE-868
Endpoint | dMMR Population |  | pMMR Population
Endpoint | KEYTRUDA with paclitaxel and carboplatin n=110 | Placebo with paclitaxel and carboplatin n=112 | KEYTRUDA with paclitaxel and carboplatin n=294 | Placebo with paclitaxel and carboplatin n=294
PFS [Based on interim PFS analysis; the information fractions for interim analyses were 49% for dMMR and 55% for pMMR.]
Number (%) of patients with event | 26 (24%) | 57 (51%) | 91 (31%) | 124 (42%)
Median in months (95% CI) | NR (30.7, NR) | 6.5 (6.4, 8.7) | 11.1 (8.7, 13.5) | 8.5 (7.2, 8.8)
Hazard ratio [Based on the stratified Cox proportional hazard model] (95% CI) | 0.30 (0.19, 0.48) |  | 0.60 (0.46, 0.78)
p-Value [Based on the stratified log-rank test] | <0.0001 |  | <0.0001
NR = not reached

Figure 39: Kaplan-Meier Curve for Progression-Free Survival in KEYNOTE-868 (dMMR Population)

Figure 40: Kaplan-Meier Curve for Progression-Free Survival in KEYNOTE-868 (pMMR Population)

Lack of Effectiveness for Adjuvant Treatment of Patients with Endometrial Carcinoma

The efficacy of KEYTRUDA in combination with carboplatin and paclitaxel, with or without radiation, was investigated in KEYNOTE‑B21 (NCT04634877), a randomized, multicenter, double-blind, placebo-controlled trial in 1,095 patients with newly diagnosed, high‑risk endometrial cancer with no evidence of disease on imaging following curative intent surgery. High-risk disease was defined as any of the following (staging per FIGO 2009): Stage I/II with myometrial invasion and either non-endometrioid histology or aberrant p53 expression or p53 mutation, or Stage III/IVA. The trial did not meet the prespecified primary endpoint for investigator-assessed DFS, with a HR of 1.02 (95% CI: 0.79, 1.32).

In Combination with Lenvatinib for the Treatment of Advanced Endometrial Carcinoma That Is pMMR or Not MSI-H

The efficacy of KEYTRUDA in combination with lenvatinib was investigated in KEYNOTE-775 (NCT03517449), a multicenter, open-label, randomized, active-controlled trial that enrolled 827 patients with advanced endometrial carcinoma who had been previously treated with at least one prior platinum-based chemotherapy regimen in any setting, including in the neoadjuvant and adjuvant settings. Patients with endometrial sarcoma, including carcinosarcoma, or patients who had active autoimmune disease or a medical condition that required immunosuppression were ineligible. Patients with endometrial carcinoma that were pMMR (using the VENTANA MMR RxDx Panel test) or not MSI-H were stratified by ECOG performance status, geographic region, and history of pelvic radiation. Patients were randomized (1:1) to one of the following treatment arms:

- KEYTRUDA 200 mg intravenously every 3 weeks in combination with lenvatinib 20 mg orally once daily.
- Investigator’s choice, consisting of either doxorubicin 60 mg/m^2 every 3 weeks or paclitaxel 80 mg/m^2 given weekly, 3 weeks on/1 week off.

Treatment with KEYTRUDA and lenvatinib continued until RECIST v1.1-defined progression of disease as verified by BICR, unacceptable toxicity, or for KEYTRUDA, a maximum of 24 months. Treatment was permitted beyond RECIST v1.1-defined disease progression if the treating investigator considered the patient to be deriving clinical benefit, and the treatment was tolerated. Assessment of tumor status was performed every 8 weeks. The major efficacy outcome measures were OS and PFS as assessed by BICR according to RECIST v1.1, modified to follow a maximum of 10 target lesions and a maximum of 5 target lesions per organ. Additional efficacy outcome measures included ORR and DoR, as assessed by BICR.

Among the 697 pMMR patients, 346 patients were randomized to KEYTRUDA in combination with lenvatinib, and 351 patients were randomized to investigator’s choice of doxorubicin (n=254) or paclitaxel (n=97). The pMMR population characteristics were: median age of 65 years (range: 30 to 86), 52% age 65 or older; 62% White, 22% Asian, and 3% Black; 60% ECOG PS of 0 and 40% ECOG PS of 1. The histologic subtypes were endometrioid carcinoma (55%), serous (30%), clear cell carcinoma (7%), mixed (4%), and other (3%). All 697 of these patients received prior systemic therapy for endometrial carcinoma: 67% had one, 30% had two, and 3% had three or more prior systemic therapies. Thirty-seven percent of patients received only prior neoadjuvant or adjuvant therapy.

Efficacy results for the pMMR or not MSI-H patients are summarized in Table 104 and Figures 41 and 42.

Table 104: Efficacy Results in KEYNOTE-775
 | Endometrial Carcinoma (pMMR or not MSI-H)
Endpoint | KEYTRUDA 200 mg every 3 weeks and Lenvatinib n=346 | Doxorubicin or Paclitaxel n=351
OS
Number (%) of patients with event | 165 (48%) | 203 (58%)
Median in months (95% CI) | 17.4 (14.2, 19.9) | 12.0 (10.8, 13.3)
Hazard ratio [Based on the stratified Cox regression model] (95% CI) | 0.68 (0.56, 0.84)
p-Value [Based on stratified log-rank test] | 0.0001
PFS
Number (%) of patients with event | 247 (71%) | 238 (68%)
Median in months (95% CI) | 6.6 (5.6, 7.4) | 3.8 (3.6, 5.0)
Hazard ratio (95% CI) | 0.60 (0.50, 0.72)
p-Value | <0.0001
Objective Response Rate
ORR [Response: Best objective response as confirmed complete response or partial response] (95% CI) | 30% (26, 36) | 15% (12, 19)
Complete response rate | 5% | 3%
Partial response rate | 25% | 13%
p-Value [Based on Miettinen and Nurminen method stratified by ECOG performance status, geographic region, and history of pelvic radiation] | <0.0001
Duration of Response | n=105 | n=53
Median in months (range) | 9.2 (1.6+, 23.7+) | 5.7 (0.0+, 24.2+)

Figure 41: Kaplan-Meier Curve for Overall Survival in KEYNOTE-775 (pMMR or Not MSI-H)

Figure 42: Kaplan-Meier Curve for Progression-Free Survival in KEYNOTE-775 (pMMR or Not MSI-H)

As a Single Agent for the Treatment of Advanced MSI-H or dMMR Endometrial Carcinoma

The efficacy of KEYTRUDA was investigated in KEYNOTE-158 (NCT02628067), a multicenter, non-randomized, open-label, multi-cohort trial. The trial enrolled 90 patients with unresectable or metastatic MSI-H or dMMR endometrial carcinoma in Cohorts D and K. MSI or MMR tumor status was determined using polymerase chain reaction (PCR) or immunohistochemistry (IHC), respectively. Patients with autoimmune disease or a medical condition that required immunosuppression were ineligible. Patients received KEYTRUDA 200 mg intravenously every 3 weeks until unacceptable toxicity or documented disease progression. Patients treated with KEYTRUDA without disease progression could be treated for up to 24 months. Assessment of tumor status was performed every 9 weeks for the first 12 months, and every 12 weeks thereafter. The major efficacy outcome measures were ORR and DoR as assessed by BICR according to RECIST v1.1, modified to follow a maximum of 10 target lesions and a maximum of 5 target lesions per organ.

Among the 90 patients evaluated, the baseline characteristics were: median age of 64 years (range: 42 to 86); 83% White, 8% Asian, and 3% Black; 12% Hispanic or Latino; 39% ECOG PS of 0 and 61% ECOG PS of 1; 96% had M1 disease and 4% had M0 disease at study entry; and 51% had one and 48% had two or more prior lines of therapy. Nine patients received only adjuvant therapy and one patient received only neoadjuvant and adjuvant therapy before participating in the study.

Efficacy results are summarized in Table 105.

Table 105: Efficacy Results in Patients with Advanced MSI-H or dMMR Endometrial Carcinoma in KEYNOTE-158
Endpoint | KEYTRUDA n=90 [Median follow-up time of 16.0 months (range 0.5 to 62.1 months)]
Objective Response Rate
ORR (95% CI) | 46% (35, 56)
Complete response rate | 12%
Partial response rate | 33%
Duration of Response | n=41
Median in months (range) | NR (2.9, 55.7+)
% with duration ≥12 months | 68%
% with duration ≥24 months | 44%
+ Denotes ongoing response
NR = not reached

14.18 Tumor Mutational Burden-High Cancer

The efficacy of KEYTRUDA was investigated in a prospectively-planned retrospective analysis of 10 cohorts (A through J) of patients with various previously treated unresectable or metastatic solid tumors with high tumor mutation burden (TMB-H) who were enrolled in a multicenter, non-randomized, open-label trial, KEYNOTE-158 (NCT02628067). The trial excluded patients who previously received an anti-PD-1 or other immune-modulating monoclonal antibody, or who had an autoimmune disease, or a medical condition that required immunosuppression. Patients received KEYTRUDA 200 mg intravenously every 3 weeks until unacceptable toxicity or documented disease progression. Assessment of tumor status was performed every 9 weeks for the first 12 months and every 12 weeks thereafter.

The statistical analysis plan pre-specified ≥10 and ≥13 mutations per megabase using the FoundationOne CDx assay as cutpoints to assess TMB. Testing of TMB was blinded with respect to clinical outcomes. The major efficacy outcome measures were ORR and DoR in patients who received at least one dose of KEYTRUDA as assessed by BICR according to RECIST v1.1, modified to follow a maximum of 10 target lesions and a maximum of 5 target lesions per organ.

In KEYNOTE-158, 1050 patients were included in the efficacy analysis population. TMB was analyzed in the subset of 790 patients with sufficient tissue for testing based on protocol-specified testing requirements. Of the 790 patients, 102 (13%) had tumors identified as TMB-H, defined as TMB ≥10 mutations per megabase. Among the 102 patients with TMB-H advanced solid tumors, the study population characteristics were: median age of 61 years (range: 27 to 80), 34% age 65 or older; 34% male; 81% White; and 41% ECOG PS of 0 and 58% ECOG PS of 1. Fifty-six percent of patients had at least two prior lines of therapy.

Efficacy results are summarized in Tables 106 and 107.

Table 106: Efficacy Results for Patients with TMB-H Cancer in KEYNOTE-158
Endpoint | KEYTRUDA 200 mg every 3 weeks
 | TMB ≥10 mut/Mb n=102 [Median follow-up time of 11.1 months] | TMB ≥13 mut/Mb n=70
Objective Response Rate
ORR (95% CI) | 29% (21, 39) | 37% (26, 50)
Complete response rate | 4% | 3%
Partial response rate | 25% | 34%
Duration of Response | n=30 | n=26
Median in months (range) [From product-limit (Kaplan-Meier) method for censored data] | NR (2.2+, 34.8+) | NR (2.2+, 34.8+)
% with duration ≥12 months | 57% | 58%
% with duration ≥24 months | 50% | 50%
+ Denotes ongoing response
NR = not reached

Table 107: Response by Tumor Type (TMB ≥10 mut/Mb)
 |  | Objective Response Rate |  | Duration of Response range
 | N | n (%) | 95% CI | (months)
Overall [No TMB-H patients were identified in the cholangiocarcinoma cohort] | 102 | 30 (29%) | (21%, 39%) | (2.2+, 34.8+)
Small cell lung cancer | 34 | 10 (29%) | (15%, 47%) | (4.1, 32.5+)
Cervical cancer | 16 | 5 (31%) | (11%, 59%) | (3.7+, 34.8+)
Endometrial cancer | 15 | 7 (47%) | (21%, 73%) | (8.4+, 33.9+)
Anal cancer | 14 | 1 (7%) | (0.2%, 34%) | 18.8+
Vulvar cancer | 12 | 2 (17%) | (2%, 48%) | (8.8, 11.0)
Neuroendocrine cancer | 5 | 2 (40%) | (5%, 85%) | (2.2+, 32.6+)
Salivary cancer | 3 | PR, SD, PD |  | 31.3+
Thyroid cancer | 2 | CR, CR |  | (8.2, 33.2+)
Mesothelioma cancer | 1 | PD
CR = complete response
PR = partial response
SD = stable disease
PD = progressive disease

In an exploratory analysis in 32 patients enrolled in KEYNOTE-158 whose cancer had TMB ≥10 mut/Mb and <13 mut/Mb, the ORR was 13% (95% CI: 4%, 29%), including two complete responses and two partial responses.

14.19 Cutaneous Squamous Cell Carcinoma

The efficacy of KEYTRUDA was investigated in patients with recurrent or metastatic cSCC or locally advanced cSCC enrolled in KEYNOTE-629 (NCT03284424), a multicenter, multi-cohort, non-randomized, open-label trial. The trial excluded patients with autoimmune disease or a medical condition that required immunosuppression.

Patients received KEYTRUDA 200 mg intravenously every 3 weeks until documented disease progression, unacceptable toxicity, or a maximum of 24 months. Patients with initial radiographic disease progression could receive additional doses of KEYTRUDA during confirmation of progression unless disease progression was symptomatic, rapidly progressive, required urgent intervention, or occurred with a decline in performance status.

Assessment of tumor status was performed every 6 weeks during the first year, and every 9 weeks during the second year. The major efficacy outcome measures were ORR and DoR as assessed by BICR according to RECIST v1.1, modified to follow a maximum of 10 target lesions and a maximum of 5 target lesions per organ.

Among the 105 patients with recurrent or metastatic cSCC treated, the study population characteristics were: median age of 72 years (range: 29 to 95), 71% age 65 or older; 76% male; 70% White, 25% race unknown; 34% ECOG PS of 0 and 66% ECOG PS of 1. Forty-five percent of patients had locally recurrent only cSCC, 24% had metastatic only cSCC, and 31% had both locally recurrent and metastatic cSCC. Eighty-seven percent received one or more prior lines of therapy; 73% received prior radiation therapy.

Among the 54 patients with locally advanced cSCC treated, the study population characteristics were: median age of 76 years (range: 35 to 95), 80% age 65 or older; 72% male; 83% White, 13% race unknown; 41% ECOG PS of 0 and 59% ECOG PS of 1. Twenty-two percent received one or more prior lines of therapy; 63% received prior radiation therapy.

Efficacy results are summarized in Table 108.

Table 108: Efficacy Results in KEYNOTE-629
Endpoint | KEYTRUDA Recurrent or Metastatic cSCC n=105 | KEYTRUDA Locally Advanced cSCC n=54
Objective Response Rate
ORR (95% CI) | 35% (26, 45) | 52% (38, 66)
Complete response rate | 12% | 22%
Partial response rate | 23% | 30%
Duration of Response [Median follow-up time: recurrent or metastatic cSCC: 23.8 months; locally advanced cSCC: 48.0 months] | n=37 | n=28
Median in months (range) | NR (2.7, 64.2+) | 47.2 (1.0+, 49.9+)
% with duration ≥6 months | 76% | 89%
% with duration ≥12 months | 68% | 75%
+ Denotes ongoing response

14.20 Triple-Negative Breast Cancer

Neoadjuvant and Adjuvant Treatment of High-Risk Early-Stage TNBC

The efficacy of KEYTRUDA in combination with neoadjuvant chemotherapy followed by surgery and continued adjuvant treatment with KEYTRUDA as a single agent was investigated in KEYNOTE-522 (NCT03036488), a randomized (2:1), multicenter, double-blind, placebo-controlled trial conducted in 1174 patients with newly diagnosed previously untreated high-risk early-stage TNBC (tumor size >1 cm but ≤2 cm in diameter with nodal involvement or tumor size >2 cm in diameter regardless of nodal involvement). Patients were enrolled regardless of tumor PD-L1 expression. Patients with active autoimmune disease that required systemic therapy within two years of treatment or a medical condition that required immunosuppression were ineligible. Randomization was stratified by nodal status (positive vs. negative), tumor size (T1/T2 vs. T3/T4), and choice of carboplatin (dosed every 3 weeks vs. weekly).

Patients were randomized (2:1) to one of the following two treatment arms; all study medications were administered intravenously:

- Arm 1:
  - Four cycles of preoperative KEYTRUDA 200 mg every 3 weeks on Day 1 of cycles 1-4 of treatment regimen in combination with:
    - Carboplatin
      - AUC 5 mg/mL/min every 3 weeks on Day 1 of cycles 1-4 of treatment regimen
        -or-
      - AUC 1.5 mg/mL/min every week on Days 1, 8, and 15 of cycles 1-4 of treatment regimen
        -and-
    - Paclitaxel 80 mg/m^2 every week on Days 1, 8, and 15 of cycles 1-4 of treatment regimen
  - Followed by four additional cycles of preoperative KEYTRUDA 200 mg every 3 weeks on Day 1 of cycles 5-8 of treatment regimen in combination with:
    - Doxorubicin 60 mg/m^2 -or- epirubicin 90 mg/m^2 every 3 weeks on Day 1 of cycles 5-8 of treatment regimen -and-
    - Cyclophosphamide 600 mg/m^2 every 3 weeks on Day 1 of cycles 5-8 of treatment regimen
  - Following surgery, nine cycles of KEYTRUDA 200 mg every 3 weeks were administered.
- Arm 2:
  - Four cycles of preoperative placebo every 3 weeks on Day 1 of cycles 1-4 of treatment regimen in combination with:
    - Carboplatin
      - AUC 5 mg/mL/min every 3 weeks on Day 1 of cycles 1-4 of treatment regimen
        -or-
      - AUC 1.5 mg/mL/min every week on Days 1, 8, and 15 of cycles 1-4 of treatment regimen
        -and-
    - Paclitaxel 80 mg/m^2 every week on Days 1, 8, and 15 of cycles 1-4 of treatment regimen
  - Followed by four cycles of preoperative placebo every 3 weeks on Day 1 of cycles 5-8 of treatment regimen in combination with:
    - Doxorubicin 60 mg/m^2 -or- epirubicin 90 mg/m^2 every 3 weeks on Day 1 of cycles 5-8 of treatment regimen -and-
    - Cyclophosphamide 600 mg/m^2 every 3 weeks on Day 1 of cycles 5-8 of treatment regimen
  - Following surgery, nine cycles of placebo every 3 weeks were administered.

The trial was not designed to isolate the effect of KEYTRUDA in each phase (neoadjuvant or adjuvant) of treatment.

The main efficacy outcomes were pCR rate and EFS. pCR was defined as absence of invasive cancer in the breast and lymph nodes (ypT0/Tis ypN0) and was assessed by the blinded local pathologist at the time of definitive surgery. EFS was defined as the time from randomization to the first occurrence of any of the following events: progression of disease that precludes definitive surgery, local or distant recurrence, second primary malignancy, or death due to any cause. An additional efficacy outcome was overall survival (OS).

The study population characteristics were: median age of 49 years (range: 22 to 80), 11% age 65 or older; 99.9% female; 64% White, 20% Asian, 4.5% Black, and 1.8% American Indian or Alaska Native; 87% ECOG PS of 0 and 13% ECOG PS of 1; 56% were pre-menopausal status and 44% were post-menopausal status; 7% were primary Tumor 1 (T1), 68% T2, 19% T3, and 7% T4; 49% were nodal involvement 0 (N0), 40% N1, 11% N2, and 0.2% N3; 75% of patients were overall Stage II and 25% were Stage III.

Statistically significant improvements in pCR, EFS, and OS were demonstrated at pre-specified interim analyses for patients randomized to KEYTRUDA in combination with chemotherapy followed by KEYTRUDA as a single agent compared with patients randomized to placebo in combination with chemotherapy followed by placebo alone.

Table 109 and Figures 43 and 44 summarize the efficacy results for KEYNOTE-522.

Table 109: Efficacy Results in KEYNOTE-522
Endpoint | KEYTRUDA 200 mg every 3 weeks with chemotherapy/KEYTRUDA n=784 | Placebo with chemotherapy/Placebo n=390
pCR (ypT0/Tis ypN0) [Based on the entire intention-to-treat population n=1174 patients]
Number of patients with pCR | 494 | 217
pCR rate (%), (95% CI) | 63.0 (59.5, 66.4) | 55.6 (50.6, 60.6)
Treatment difference (%) estimate (95% CI) [Based on a pre-specified pCR interim analysis in n=602 patients, the pCR rate difference was statistically significant (p=0.00055 compared to a significance level of 0.003).] , [Based on Miettinen and Nurminen method stratified by nodal status, tumor size, and choice of carboplatin] | 7.5 (1.6, 13.4)
EFS
Number of patients with event (%) | 123 (16%) | 93 (24%)
Hazard ratio (95% CI) [Based on stratified Cox regression model] | 0.63 (0.48, 0.82)
p-Value [Based on a pre-specified EFS interim analysis (compared to a significance level of 0.0052)] , [Based on log-rank test stratified by nodal status, tumor size, and choice of carboplatin] | 0.00031
OS
Number of patients with event (%) | 115 (15%) | 85 (22%)
Hazard ratio (95% CI) | 0.66 (0.50, 0.87)
p-Value, [Based on a pre-specified OS interim analysis (compared to a significance level of 0.0050)] | 0.00150

Figure 43: Kaplan-Meier Curve for Event-Free Survival in KEYNOTE-522

Figure 44: Kaplan-Meier Curve for Overall Survival in KEYNOTE-522

Locally Recurrent Unresectable or Metastatic TNBC for Tumors Expressing PD-L1 (CPS≥ 10)

The efficacy of KEYTRUDA in combination with paclitaxel, paclitaxel protein-bound, or gemcitabine and carboplatin was investigated in KEYNOTE-355 (NCT02819518), a multicenter, double-blind, randomized, placebo-controlled trial conducted in 847 patients with locally recurrent unresectable or metastatic TNBC, regardless of tumor PD-L1 expression, who had not been previously treated with chemotherapy in the metastatic setting. Patients with active autoimmune disease that required systemic therapy within 2 years of treatment or a medical condition that required immunosuppression were ineligible. Randomization was stratified by chemotherapy treatment (paclitaxel or paclitaxel protein-bound vs. gemcitabine and carboplatin), tumor PD-L1 expression (CPS ≥1 vs. CPS <1) according to the PD-L1 IHC 22C3 pharmDx assay, and prior treatment with the same class of chemotherapy in the neoadjuvant setting (yes vs. no).

Patients were randomized (2:1) to one of the following treatment arms; all study medications were administered via intravenous infusion:

- KEYTRUDA 200 mg on Day 1 every 3 weeks in combination with paclitaxel protein-bound 100 mg/m^2 on Days 1, 8 and 15 every 28 days, paclitaxel 90 mg/m^2 on Days 1, 8, and 15 every 28 days, or gemcitabine 1000 mg/m^2 and carboplatin AUC 2 mg/mL/min on Days 1 and 8 every 21 days.
- Placebo on Day 1 every 3 weeks in combination with paclitaxel protein-bound 100 mg/m^2 on Days 1, 8 and 15 every 28 days, paclitaxel 90 mg/m^2 on Days 1, 8, and 15 every 28 days, or gemcitabine 1000 mg/m^2 and carboplatin AUC 2 mg/mL/min on Days 1 and 8 every 21 days.

Assessment of tumor status was performed at Weeks 8, 16, and 24, then every 9 weeks for the first year, and every 12 weeks thereafter. The main efficacy outcome measures were OS and PFS as assessed by BICR according to RECIST v1.1, modified to follow a maximum of 10 target lesions and a maximum of 5 target lesions per organ, tested in the subgroup of patients with CPS ≥10. Additional efficacy outcome measures were ORR and DoR as assessed by BICR.

The study population characteristics for patients were: median age of 53 years (range: 22 to 85), 21% age 65 or older; 100% female; 68% White, 21% Asian, and 4% Black; 60% ECOG PS of 0 and 40% ECOG PS of 1; and 68% were post-menopausal status. Seventy-five percent of patients had tumor PD-L1 expression CPS ≥1 and 38% had tumor PD-L1 expression CPS ≥10.

Table 110 and Figures 45 and 46 summarize the efficacy results for KEYNOTE-355.

Table 110: Efficacy Results in KEYNOTE-355 (CPS ≥10)
Endpoint | KEYTRUDA 200 mg every 3 weeks with chemotherapy n=220 | Placebo every 3 weeks with chemotherapy n=103
OS [Based on the pre-specified final analysis]
Number of patients with event (%) | 155 (70%) | 84 (82%)
Median in months (95% CI) | 23 (19.0, 26.3) | 16.1 (12.6, 18.8)
Hazard ratio [Based on stratified Cox regression model] (95% CI) | 0.73 (0.55, 0.95)
p-Value [One-sided p-Value based on stratified log-rank test (compared to a significance level of 0.0113)] | 0.0093
PFS [Based on a pre-specified interim analysis]
Number of patients with event (%) | 136 (62%) | 79 (77%)
Median in months (95% CI) | 9.7 (7.6, 11.3) | 5.6 (5.3, 7.5)
Hazard ratio (95% CI) | 0.65 (0.49, 0.86)
p-Value [One-sided p-Value based on stratified log-rank test (compared to a significance level of 0.00411)] | 0.0012
Objective Response Rate (Confirmed)
ORR (95% CI) | 53% (46, 59) | 41% (31, 51)
Complete response rate | 17% | 14%
Partial response rate | 35% | 27%
Duration of Response | n=116 | n=42
Median in months (95% CI) | 12.8 (9.9, 25.9) | 7.3 (5.5, 15.4)

Figure 45: Kaplan-Meier Curve for Overall Survival in KEYNOTE-355 (CPS ≥10)

Figure 46: Kaplan-Meier Curve for Progression-Free Survival in KEYNOTE-355 (CPS ≥10)

14.21 Ovarian Cancer

The efficacy of KEYTRUDA in combination with paclitaxel, with or without bevacizumab, was evaluated in KEYNOTE-B96 (NCT05116189), a multicenter, randomized, double-blind, placebo-controlled trial that enrolled 643 patients with platinum-resistant, epithelial ovarian, fallopian tube, or primary peritoneal carcinoma who received one or two prior lines of systemic therapy for ovarian carcinoma. Patients must have received at least one line of platinum-based chemotherapy for ovarian cancer with radiographic evidence of disease progression within 6 months after the last dose. Prior therapy with an anti-PD-1/PD-L1 inhibitor, PARP inhibitor, or bevacizumab was permitted. Patients were enrolled regardless of PD-L1 tumor expression status. Patients with autoimmune disease that required systemic therapy within 2 years of treatment or a medical condition that required immunosuppression were ineligible. Randomization was stratified by investigator decision to use bevacizumab, geographic region (U.S. or European Union or Rest of World), and PD-L1 status according to the PD-L1 IHC 22C3 pharmDx assay (CPS <1 or CPS 1 to <10 or CPS ≥10). Patients were randomized (1:1) to one of the two treatment groups:

- KEYTRUDA 400 mg every 6 weeks plus paclitaxel 80 mg/m^2 with or without bevacizumab 10 mg/kg
- Placebo every 6 weeks plus paclitaxel 80 mg/m^2 with or without bevacizumab 10 mg/kg

All study medications were administered as an intravenous infusion. KEYTRUDA 400 mg or placebo were administered on Day 1 of each 6-week treatment cycle and paclitaxel 80 mg/m^2 was administered on Days 1, 8, and 15 of each 3-week treatment cycle. The option to use bevacizumab was by investigator choice prior to randomization. Bevacizumab 10 mg/kg was administered on Day 1 of a 2-week treatment cycle. Treatment with KEYTRUDA continued until RECIST v1.1-defined progression of disease, unacceptable toxicity, or a maximum of 24 months. Administration of KEYTRUDA was permitted beyond RECIST-defined disease progression if the patient was clinically stable and considered to be deriving clinical benefit by the investigator. Assessment of tumor status was performed every 9 weeks for the first year, followed by every 12 weeks thereafter. The major efficacy outcome measure was PFS as assessed by investigator according to RECIST v1.1. An additional efficacy outcome measure was OS.

Among the 643 patients randomized, 466 patients (72%) had tumors expressing PD-L1 with a CPS ≥1. The population characteristics of these 466 patients were: median age of 62 years (range: 37 to 85), 38% age 65 or older; 67% White, 20% Asian, 8% Missing, 3% Multiple, 2% Black, 0.4% Native Hawaiian or other Pacific Islander; 13% Hispanic or Latino; 55% and 44% ECOG performance status of 0 or 1, respectively; 73% received bevacizumab as study treatment; 36% of patients had received one prior line and 64% had received two prior lines of therapy; prior systemic therapy included: 46% with bevacizumab; 39% with a PARP inhibitor, or 3% with an anti-PD-1/PD-L1 inhibitor. The platinum-free interval following the most recent line of therapy was <3 months in 47% of patients, and 3 to 6 months in 53% of patients.

The study demonstrated statistically significant improvement in PFS and OS for patients randomized to KEYTRUDA in combination with paclitaxel with or without bevacizumab compared to placebo in combination with paclitaxel with or without bevacizumab in patients whose tumors expressed PD-L1 CPS ≥1. Efficacy results are summarized in Table 111 and Figures 47 and 48.

Table 111: Efficacy Results in KEYNOTE-B96 (CPS ≥1)
Endpoint | KEYTRUDA 400 mg every 6 weeks plus paclitaxel with or without bevacizumab n=234 | Placebo plus paclitaxel with or without bevacizumab n=232
PFS
Number of patients with event (%) | 162 (69) | 180 (78)
Median in months (95% CI) | 8.3 (7.0, 9.4) | 7.2 (6.2, 8.1)
Hazard ratio (95% CI) | 0.72 (0.58, 0.89)
p-Value | 0.0014 [Based on stratified log-rank test (p-Value [one-sided] is compared to an alpha boundary of 0.0116)]
OS
Number of patients with event (%) | 157 (67) | 175 (75)
Median in months (95% CI) | 18.2 (15.3, 21.0) | 14.0 (12.5, 16.1)
Hazard ratio (95% CI) | 0.76 (0.61, 0.94)
p-Value | 0.0053 [Based on stratified log-rank test (p-Value [one sided] is compared to an alpha boundary of 0.0083)]

Figure 47: Kaplan-Meier Curve for Progression-Free Survival in KEYNOTE-B96 (CPS ≥1)

Figure 48: Kaplan-Meier Curve for Overall Survival in KEYNOTE-B96 (CPS ≥1)

16 HOW SUPPLIED/STORAGE AND HANDLING

KEYTRUDA injection (clear to slightly opalescent, colorless to slightly yellow solution):

Carton containing one 100 mg/4 mL (25 mg/mL), single-dose vial (NDC 0006-3026-02)
Carton containing two 100 mg/4 mL (25 mg/mL), single-dose vials (NDC 0006-3026-04)

STORAGE AND HANDLING

Store vials under refrigeration at 2°C to 8°C (36°F to 46°F) in original carton to protect from light. Do not freeze. Do not shake.

17 PATIENT COUNSELING INFORMATION

Advise the patient to read the FDA-authorized patient labeling (Medication Guide).

Immune-Mediated Adverse Reactions

- Inform patients of the risk of immune-mediated adverse reactions that may be severe or fatal, may occur after discontinuation of treatment, and may require corticosteroid treatment and interruption or discontinuation of KEYTRUDA. These reactions may include:
  - Pneumonitis: Advise patients to contact their healthcare provider immediately for new or worsening cough, chest pain, or shortness of breath [see Warnings and Precautions (5.1)].
  - Colitis: Advise patients to contact their healthcare provider immediately for diarrhea or severe abdominal pain [see Warnings and Precautions (5.1)].
  - Hepatitis: Advise patients to contact their healthcare provider immediately for jaundice, severe nausea or vomiting, or easy bruising or bleeding [see Warnings and Precautions (5.1)].
  - Endocrinopathies: Advise patients to contact their healthcare provider immediately for signs or symptoms of adrenal insufficiency, hypophysitis, hypothyroidism, hyperthyroidism, or Type 1 diabetes mellitus [see Warnings and Precautions (5.1)].
  - Nephritis: Advise patients to contact their healthcare provider immediately for signs or symptoms of nephritis [see Warnings and Precautions (5.1)].
  - Severe skin reactions: Advise patients to contact their healthcare provider immediately for any signs or symptoms of severe skin reactions, SJS or TEN [see Warnings and Precautions (5.1)].
  - Other immune-mediated adverse reactions:
    - Advise patients that immune-mediated adverse reactions can occur and may involve any organ system, and to contact their healthcare provider immediately for any new or worsening signs or symptoms [see Warnings and Precautions (5.1)].
    - Advise patients of the risk of solid organ transplant rejection and other transplant (including corneal graft) rejection. Advise patients to contact their healthcare provider immediately for signs or symptoms of organ transplant rejection and other transplant (including corneal graft) rejection [see Warnings and Precautions (5.1)].

Infusion-Related Reactions

- Advise patients to contact their healthcare provider immediately for signs or symptoms of infusion-related reactions [see Warnings and Precautions (5.2)].

Complications of Allogeneic HSCT

- Advise patients of the risk of post-allogeneic hematopoietic stem cell transplantation complications [see Warnings and Precautions (5.3)].

Embryo-Fetal Toxicity

- Advise females of reproductive potential of the potential risk to a fetus and to inform their healthcare provider of a known or suspected pregnancy [see Warnings and Precautions (5.5), Use in Specific Populations (8.1, 8.3)].
- Advise females of reproductive potential to use effective contraception during treatment with KEYTRUDA and for 4 months after the last dose [see Warnings and Precautions (5.5), Use in Specific Populations (8.1, 8.3)].

Lactation

- Advise women not to breastfeed during treatment with KEYTRUDA and for 4 months after the last dose [see Use in Specific Populations (8.2)].

Laboratory Tests

- Advise patients of the importance of keeping scheduled appointments for blood work or other laboratory tests [see Warnings and Precautions (5.1)].

Manufactured for: Merck Sharp & Dohme LLC
Rahway, NJ 07065, USA

Manufactured by: MSD International Business GmbH
6005 Luzern, Switzerland
U.S. License No. 2405

For patent information: www.msd.com/research/patent

The trademarks depicted herein are owned by their respective companies.

Copyright © 2014-2026 Merck & Co., Inc., Rahway, NJ, USA, and its affiliates.
All rights reserved.

uspi-mk3475-iv-2602r093

MEDICATION GUIDE
KEYTRUDA® (key-true-duh)
(pembrolizumab)
injection

What is the most important information I should know about KEYTRUDA?

KEYTRUDA is a medicine that may treat certain cancers by working with your immune system. KEYTRUDA can cause your immune system to attack normal organs and tissues in any area of your body and can affect the way they work. These problems can sometimes become severe or life-threatening and can lead to death. You can have more than one of these problems at the same time. These problems may happen anytime during treatment or even after your treatment has ended.

Call or see your healthcare provider right away if you develop any new or worsening signs or symptoms, including:

Lung problems

- cough

- shortness of breath

- chest pain

Intestinal problems

- diarrhea (loose stools) or more frequent bowel movements than usual
- stools that are black, tarry, sticky, or have blood or mucus
- severe stomach-area (abdomen) pain or tenderness

Liver problems

- yellowing of your skin or the whites of your eyes
- severe nausea or vomiting
- pain on the right side of your stomach area (abdomen)

- dark urine (tea colored)
- bleeding or bruising more easily than normal

Hormone gland problems

- headaches that will not go away or unusual headaches
- eye sensitivity to light
- eye problems
- rapid heartbeat
- increased sweating
- extreme tiredness
- weight gain or weight loss
- feeling more hungry or thirsty than usual

- urinating more often than usual
- hair loss
- feeling cold
- constipation
- your voice gets deeper
- dizziness or fainting
- changes in mood or behavior, such as decreased sex drive, irritability, or forgetfulness

Kidney problems

- decrease in your amount of urine
- blood in your urine

- swelling of your ankles
- loss of appetite

Skin problems

- rash
- itching
- skin blistering or peeling

- painful sores or ulcers in your mouth or in your nose, throat, or genital area
- fever or flu-like symptoms
- swollen lymph nodes

Problems can also happen in other organs and tissues. These are not all of the signs and symptoms of immune system problems that can happen with KEYTRUDA. Call or see your healthcare provider right away for any new or worsening signs or symptoms, which may include:

- chest pain, irregular heartbeat, shortness of breath, swelling of ankles
- confusion, sleepiness, memory problems, changes in mood or behavior, stiff neck, balance problems, tingling or numbness of the arms or legs
- double vision, blurry vision, sensitivity to light, eye pain, changes in eyesight
- persistent or severe muscle pain or weakness, muscle cramps
- low red blood cells, bruising

Infusion reactions that can sometimes be severe or life-threatening. Signs and symptoms of infusion reactions may include:

- chills or shaking
- itching or rash
- flushing
- shortness of breath or wheezing

- dizziness
- feeling like passing out
- fever
- back pain

Rejection of a transplanted organ or tissue. Your healthcare provider should tell you what signs and symptoms you should report and monitor you depending on the type of organ or tissue transplant that you have had.

Complications, including graft-versus-host-disease (GVHD), in people who have received a bone marrow (stem cell) transplant that uses donor stem cells (allogeneic). These complications can be serious and can lead to death. These complications may happen if you underwent transplantation either before or after being treated with KEYTRUDA. Your healthcare provider will monitor you for these complications.

Getting medical treatment right away may help keep these problems from becoming more serious.

Your healthcare provider will check you for these problems during treatment with KEYTRUDA. Your healthcare provider may treat you with corticosteroid or hormone replacement medicines. Your healthcare provider may also need to delay or completely stop treatment with KEYTRUDA if you have severe side effects.

What is KEYTRUDA?

KEYTRUDA is a prescription medicine used to treat:

- a kind of skin cancer called melanoma. KEYTRUDA may be used:
  - when your melanoma has spread or cannot be removed by surgery (advanced melanoma), or
  - in adults and children 12 years of age and older with Stage IIB, Stage IIC, or Stage III melanoma, to help prevent melanoma from coming back after it and lymph nodes that contain cancer have been removed by surgery.
- a kind of lung cancer called non-small cell lung cancer (NSCLC).
  - KEYTRUDA may be used with the chemotherapy medicines pemetrexed and a platinum as your first treatment when your lung cancer:
    - has spread (advanced NSCLC), and
    - is a type called “nonsquamous”, and
    - your tumor does not have an abnormal “EGFR” or “ALK” gene.
  - KEYTRUDA may be used with the chemotherapy medicines carboplatin and either paclitaxel or paclitaxel protein-bound as your first treatment when your lung cancer:
    - has spread (advanced NSCLC), and
    - is a type called “squamous”.
  - KEYTRUDA may be used alone as your first treatment when your lung cancer:
    - has not spread outside your chest (Stage III) and you cannot have surgery or chemotherapy with radiation or
    - your NSCLC has spread to other areas of your body (advanced NSCLC), and
    - your tumor tests positive for “PD-L1”, and
    - does not have an abnormal “EGFR” or “ALK” gene.
  - KEYTRUDA may also be used alone when:
    - you have received chemotherapy that contains platinum to treat your advanced NSCLC, and it did not work or it is no longer working, and
    - your tumor tests positive for “PD-L1”, and
    - if your tumor has an abnormal “EGFR” or “ALK” gene, you have also received an EGFR or ALK inhibitor medicine and it did not work or is no longer working.
  - KEYTRUDA may be used in combination with chemotherapy that contains platinum and another chemotherapy medicine:
    - before surgery when you have early-stage NSCLC which can be removed by surgery, and
    - then continued alone after surgery to help prevent your lung cancer from coming back.
  - KEYTRUDA may be used alone as a treatment in adults for your lung cancer:
    - to help prevent your lung cancer from coming back after your tumor(s) has been removed by surgery and you have received platinum-based chemotherapy, and
    - you have Stage IB and your tumor(s) is 4 cm or greater in size, Stage II, or Stage IIIA NSCLC.
- a kind of cancer in adults called malignant pleural mesothelioma (MPM) that affects the lining of the lungs and chest wall.
  - KEYTRUDA may be used in combination with the chemotherapy medicines pemetrexed and a platinum as your first treatment when your cancer has spread or cannot be removed by surgery (advanced MPM).
- a kind of cancer called head and neck squamous cell cancer (HNSCC).
  - KEYTRUDA may be used alone in adults with HNSCC before surgery:
    - when your cancer can be removed by surgery, has spread to nearby tissues, and your tumor tests positive for “PD-L1”, and
    - then continued in combination with radiation with or without cisplatin after surgery, and
    - then continued alone to help prevent your head and neck cancer from coming back.
  - KEYTRUDA may be used with the chemotherapy medicines fluorouracil and a platinum as your first treatment when your head and neck cancer has spread or returned and cannot be removed by surgery.
  - KEYTRUDA may be used alone as your first treatment when your head and neck cancer:
    - has spread or returned and cannot be removed by surgery, and
    - your tumor tests positive for “PD-L1”.
  - KEYTRUDA may be used alone when your head and neck cancer:
    - has spread or returned, and
    - you have received chemotherapy that contains platinum and it did not work or is no longer working.
- a kind of cancer called classical Hodgkin lymphoma (cHL):
  - in adults when:
    - your cHL has returned or
    - you have tried a treatment and it did not work, or
  - in children when:
    - you have tried a treatment and it did not work or
    - your cHL has returned after you received 2 or more types of treatment.
- a kind of cancer called primary mediastinal B-cell lymphoma (PMBCL) in adults and children when:
  - you have tried a treatment and it did not work or
  - your PMBCL has returned after you received 2 or more types of treatment.
- a kind of bladder and urinary tract cancer called urothelial cancer.
  - KEYTRUDA may be used with the medicine enfortumab vedotin in adults when your bladder or urinary tract cancer has spread or cannot be removed by surgery (locally advanced or metastatic urothelial cancer).
  - KEYTRUDA may be used alone when your bladder or urinary tract cancer:
    - has spread or cannot be removed by surgery (locally advanced or metastatic urothelial cancer), and
    - you are not able to receive chemotherapy that contains platinum (medicines called either cisplatin or carboplatin), or
    - you have received chemotherapy that contains platinum, and it did not work or is no longer working.
  - KEYTRUDA may be used with the medicine enfortumab vedotin in adults before and after the surgical removal of your bladder when:
    - your bladder cancer has spread into the muscle layer of the bladder (muscle invasive bladder cancer [MIBC]) but not to other parts of the body, and
    - you are not able to receive chemotherapy that contains cisplatin.
  - KEYTRUDA may be used alone when your cancer has not spread to nearby tissue in the bladder, but is at high-risk for spreading (high-risk non-muscle-invasive bladder cancer [NMIBC]) when:
    - your tumor is a type called “carcinoma in situ” (CIS), and
    - you have tried treatment with Bacillus Calmette-Guerin (BCG) and it did not work, and
    - you are not able to or have decided not to have surgery to remove your bladder.
- a kind of cancer that is shown by a laboratory test to be a microsatellite instability-high (MSI-H) or a mismatch repair deficient (dMMR) solid tumor. KEYTRUDA may be used in adults and children to treat:
  - cancer that has spread or cannot be removed by surgery (advanced cancer), and
  - has progressed following treatment, and you have no satisfactory treatment options.
- a kind of cancer called colon or rectal cancer. KEYTRUDA may be used when your cancer:
  - has spread or cannot be removed by surgery (advanced colon or rectal cancer), and
  - has been shown by a laboratory test to be microsatellite instability-high (MSI-H) or mismatch repair deficient (dMMR).
- a kind of stomach cancer called gastric or gastroesophageal junction (GEJ) adenocarcinoma.
  - KEYTRUDA may be used in adults in combination with the medicine trastuzumab along with fluoropyrimidine and platinum chemotherapy as your first treatment when your stomach cancer:
    - is HER2-positive, and your tumor tests positive for “PD-L1”, and
    - has spread or cannot be removed by surgery (advanced gastric cancer).
  - KEYTRUDA may be used in adults in combination with fluoropyrimidine and platinum chemotherapy as your first treatment when your stomach cancer:
    - is HER2-negative, and your tumor tests positive for “PD-L1”, and
    - has spread or cannot be removed by surgery (advanced gastric cancer).
- a kind of cancer called esophageal or certain gastroesophageal junction (GEJ) carcinomas that cannot be cured by surgery or a combination of chemotherapy and radiation therapy.
  - KEYTRUDA may be used in combination with platinum- and fluoropyrimidine-based chemotherapy medicines when your tumor tests positive for “PD-L1”.
  - KEYTRUDA may be used alone when:
    - you have received one or more types of treatment, and it did not work or it is no longer working, and
    - your tumor is a type called “squamous”, and
    - your tumor tests positive for “PD-L1”.
- a kind of cancer called cervical cancer.
  - KEYTRUDA may be used with chemotherapy and radiation therapy when your cervical cancer has spread nearby to the lower part of your vagina or to pelvic organs or has affected your kidneys (Stage III to IVA FIGO 2014 classification).
  - KEYTRUDA may be used with chemotherapy medicines, with or without the medicine bevacizumab, when:
    - your cervical cancer does not go away (persistent), has returned, or has spread (advanced cervical cancer), and
    - your tumor tests positive for “PD-L1”.
  - KEYTRUDA may be used alone when your cervical cancer:
    - has returned, or has spread (advanced cervical cancer), and
    - you have received chemotherapy, and it did not work or is no longer working, and
    - your tumor tests positive for “PD-L1”.
- a kind of liver cancer called hepatocellular carcinoma (HCC). KEYTRUDA may be used when:
  - you have HCC after having hepatitis B, and
  - you have received anti-cancer treatment that did not contain a “PD-1” or “PD-L1” blocking medicine.
- a kind of bile duct or gallbladder cancer called biliary tract cancer (BTC). KEYTRUDA may be used with chemotherapy medicines gemcitabine and cisplatin when your biliary tract cancer has spread or cannot be removed by surgery.
- a kind of skin cancer called Merkel cell carcinoma (MCC) in adults and children. KEYTRUDA may be used to treat your skin cancer when it has spread or returned.
- a kind of kidney cancer called renal cell carcinoma (RCC).
  - KEYTRUDA may be used in adults with the medicine axitinib as your first treatment when your kidney cancer has spread or cannot be removed by surgery (advanced RCC).
  - KEYTRUDA may be used in adults with the medicine lenvatinib as your first treatment when your kidney cancer has spread or cannot be removed by surgery (advanced RCC).
  - KEYTRUDA may be used alone if you are at intermediate-high or high risk of your kidney cancer (RCC) coming back after surgery to:
    - remove all or part of your kidney, or
    - remove all or part of your kidney and also surgery to remove cancer that has spread to other parts of the body (metastatic lesions).
- a kind of uterine cancer called advanced endometrial carcinoma.
  - KEYTRUDA may be used with the chemotherapy medicines carboplatin and paclitaxel, and then KEYTRUDA may be used alone, in adults:
    - when your cancer has spread (advanced), or
    - if your cancer has returned.
  - KEYTRUDA may be used with the medicine lenvatinib in adults:
    - when a laboratory test shows that your tumor is mismatch repair proficient (pMMR) or not microsatellite instability-high (MSI-H), and
    - you have received anti-cancer treatment, and it is no longer working, and
    - your cancer cannot be cured by surgery or radiation.
  - KEYTRUDA may be used alone in adults:
    - if your cancer is shown by a laboratory test to be microsatellite instability-high (MSI-H) or mismatch repair deficient (dMMR), and
    - you have received anti-cancer treatment and it is no longer working, and
    - your cancer cannot be cured by surgery or radiation.
- a kind of cancer that is shown by a test to be tumor mutational burden-high (TMB-H). KEYTRUDA may be used in adults and children to treat:
  - solid tumors that have spread or cannot be removed by surgery (advanced cancer), and
  - you have received anti-cancer treatment, and it did not work or is no longer working, and
  - you have no satisfactory treatment options.
  It is not known if KEYTRUDA is safe and effective in children with TMB-H cancers of the brain or spinal cord (central nervous system cancers).
- a kind of skin cancer called cutaneous squamous cell carcinoma (cSCC). KEYTRUDA may be used when your skin cancer:
  - has returned or spread, and
  - cannot be cured by surgery or radiation.
- a kind of cancer called triple-negative breast cancer (TNBC).
  - KEYTRUDA may be used with chemotherapy medicines as treatment before surgery and then continued alone after surgery when you:
    - have early-stage breast cancer, and
    - are at high risk of your breast cancer coming back.
  - KEYTRUDA may be used with chemotherapy medicines when your breast cancer:
    - has returned and cannot be removed by surgery or has spread, and
    - tests positive for “PD-L1”.
- a kind of cancer called ovarian cancer.
  - KEYTRUDA may be used in adults with the chemotherapy medicine paclitaxel, with or without the medicine bevacizumab, when your ovarian, fallopian tube, or primary peritoneal cancer:
    - is resistant to chemotherapy that contains platinum, and
    - tests positive for “PD-L1”, and
    - you have received 1or 2 types of treatment.

Before receiving KEYTRUDA, tell your healthcare provider about all of your medical conditions, including if you:

- have immune system problems such as Crohn’s disease, ulcerative colitis, or lupus
- have received an organ or tissue transplant, including corneal transplant
- have received or plan to receive a stem cell transplant that uses donor stem cells (allogeneic)
- have received radiation treatment to your chest area
- have a condition that affects your nervous system, such as myasthenia gravis or Guillain-Barré syndrome
- are pregnant or plan to become pregnant. KEYTRUDA can harm your unborn baby.
  Females who are able to become pregnant:
  - Your healthcare provider will give you a pregnancy test before you start treatment with KEYTRUDA.
  - You should use an effective method of birth control during treatment with KEYTRUDA and for 4 months after the last dose of KEYTRUDA. Talk to your healthcare provider about birth control methods that you can use during this time.
  - Tell your healthcare provider right away if you think you may be pregnant or if you become pregnant during treatment with KEYTRUDA.
- are breastfeeding or plan to breastfeed. It is not known if KEYTRUDA passes into your breast milk. Do not breastfeed during treatment with KEYTRUDA and for 4 months after your last dose of KEYTRUDA.

Tell your healthcare provider about all the medicines you take, including prescription and over-the-counter medicines, vitamins, and herbal supplements.

How will I receive KEYTRUDA?

- Your healthcare provider will give you KEYTRUDA into your vein through an intravenous (IV) line over 30 minutes.
- In adults, KEYTRUDA is usually given every 3 weeks or 6 weeks depending on the dose of KEYTRUDA that you are receiving.
- In children, KEYTRUDA is usually given every 3 weeks.
- Your healthcare provider will decide how many treatments you need.
- Your healthcare provider will do blood tests to check you for side effects.
- If you miss any appointments, call your healthcare provider as soon as possible to reschedule your appointment.

What are the possible side effects of KEYTRUDA?

KEYTRUDA can cause serious side effects. See “What is the most important information I should know about KEYTRUDA?”

Common side effects of KEYTRUDA when used alone include: feeling tired, pain, including pain in muscles, rash, diarrhea, fever, cough, decreased appetite, itching, shortness of breath, constipation, bones or joints and stomach-area (abdominal) pain, nausea, and low levels of thyroid hormone.

Side effects of KEYTRUDA when used alone that are more common in children than in adults include: fever, vomiting, headache, stomach area (abdominal) pain, and low levels of white blood cells.

Common side effects of KEYTRUDA when given with certain chemotherapy or chemotherapy with radiation therapy medicines include: feeling tired or weak, nausea, constipation, diarrhea, decreased appetite, rash, vomiting, cough, trouble breathing, fever, hair loss, inflammation of the nerves that may cause pain, weakness, and paralysis in the arms and legs, swelling of the lining of the mouth, nose, eyes, throat, intestines, or vagina, mouth sores, headache, weight loss, stomach-area (abdominal) pain, joint and muscle pain, trouble sleeping, blisters or rash on the palms of your hands and soles of your feet, urinary tract infection, low levels of thyroid hormone, skin irritation in the radiation area, trouble swallowing and dry mouth.

Common side effects of KEYTRUDA when given with chemotherapy and bevacizumab include: tingling or numbness of the arms or legs, hair loss, low red blood cell count, feeling tired or weak, nausea, low white blood cell count, diarrhea, high blood pressure, decreased platelet count, constipation, joint aches, vomiting, urinary tract infection, rash, low levels of thyroid hormone, decreased appetite, fever, mouth sores and nosebleed.

Common side effects of KEYTRUDA when given with axitinib include: diarrhea, feeling tired or weak, high blood pressure, liver problems, low levels of thyroid hormone, decreased appetite, blisters or rash on the palms of your hands and soles of your feet, nausea, mouth sores or swelling of the lining of the mouth, nose, eyes, throat, intestines, or vagina, hoarseness, rash, cough, and constipation.

Common side effects of KEYTRUDA when given with lenvatinib include: low levels of thyroid hormone, high blood pressure, feeling tired, diarrhea, joint and muscle pain, nausea, decreased appetite, vomiting, mouth sores, weight loss, stomach-area (abdominal) pain, urinary tract infection, protein in your urine, constipation, headache, bleeding, blisters or rash on the palms of your hands and soles of your feet, hoarseness, rash, liver problems, and kidney problems.

Common side effects of KEYTRUDA when given with enfortumab vedotin include: rash, tingling or numbness of the arms or legs, feeling tired, itching, diarrhea, hair loss, weight loss, decreased appetite, dry eye, nausea, constipation, changes in sense of taste, and urinary tract infection.

These are not all the possible side effects of KEYTRUDA.

Call your doctor for medical advice about side effects. You may report side effects to FDA at 1-800-FDA-1088.

General information about the safe and effective use of KEYTRUDA

Medicines are sometimes prescribed for purposes other than those listed in a Medication Guide. You can ask your pharmacist or healthcare provider for information about KEYTRUDA that is written for health professionals.

What are the ingredients in KEYTRUDA?

Active ingredient: pembrolizumab

Inactive ingredients: L-histidine, polysorbate 80, sucrose, and Water for Injection.

Manufactured for: Merck Sharp & Dohme LLC
Rahway, NJ 07065, USA
Manufactured by: MSD International Business GmbH
6005 Luzern, Switzerland

U.S. License No. 2405
For patent information: www.msd.com/research/patent
Copyright © 2014-2026 Merck & Co., Inc., Rahway, NJ, USA, and its affiliates.
All rights reserved.
usmg-mk3475-iv-2602r073
For more information, go to www.keytruda.com.

This Medication Guide has been approved by the U.S. Food and Drug Administration.

Revised: February 2026

PRINCIPAL DISPLAY PANEL - 50 mg Vial Carton

NDC 0006-3029-02

Keytruda®
(pembrolizumab)
for Injection

50 mg /vial

For Intravenous Infusion Only

Dispense the enclosed Medication Guide to each patient.

Sterile lyophilized powder must be reconstituted with Sterile Water for
Injection, USP. Reconstituted solution requires further dilution prior
to administration.

Rx only

Single-dose vial. Discard unused portion.

PRINCIPAL DISPLAY PANEL - 100 mg/4 mL Vial Carton

NDC 0006-3026-02

Keytruda®
(pembrolizumab)
Injection

100 mg /4 mL
(25 mg/mL)

For Intravenous Infusion Only

Dispense the enclosed Medication Guide to each patient.

Requires dilution prior to administration.

Rx only
Single-dose vial. Discard unused portion.